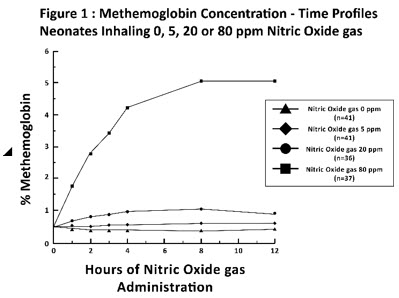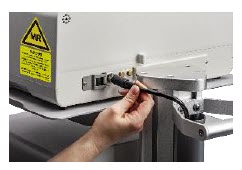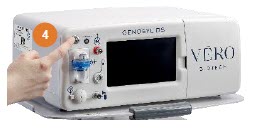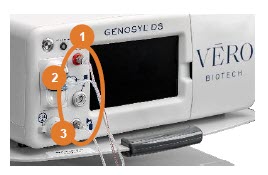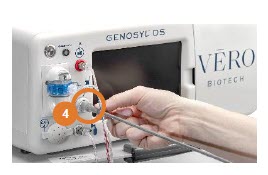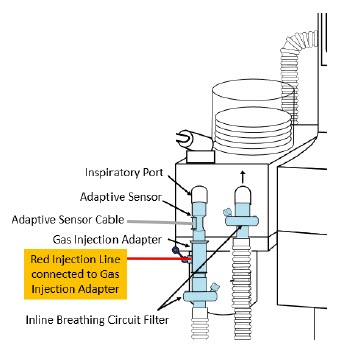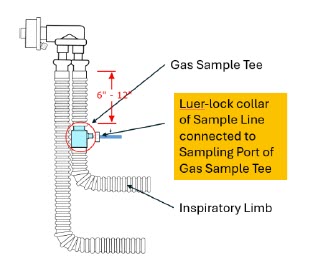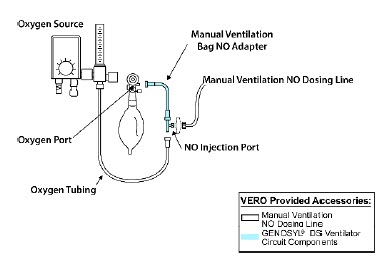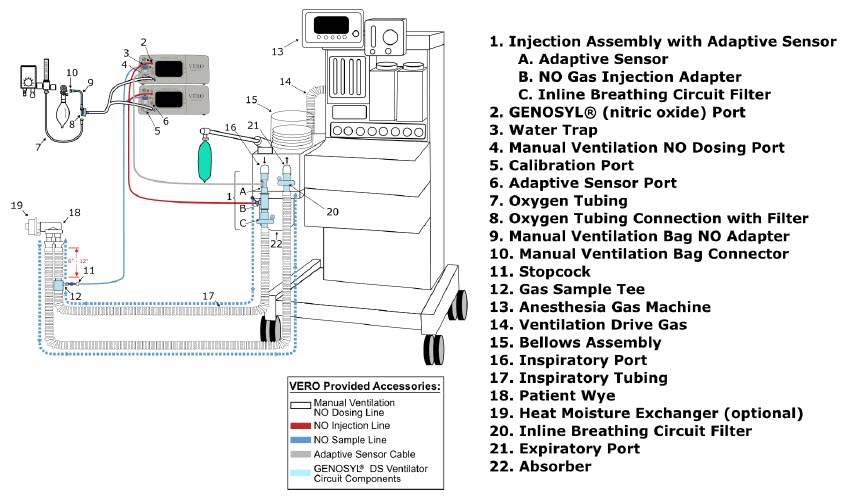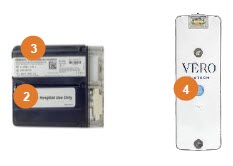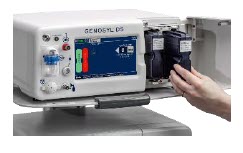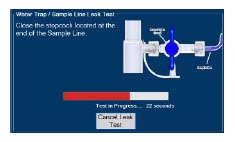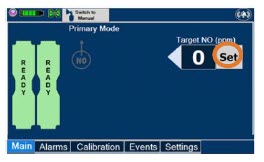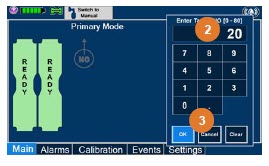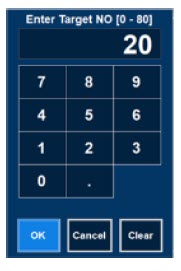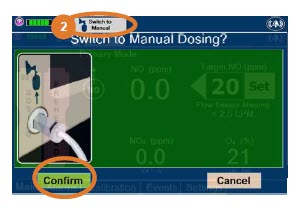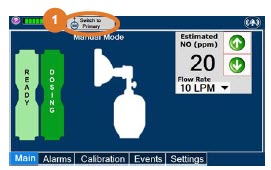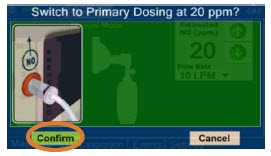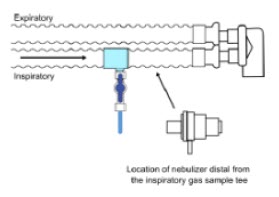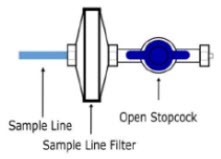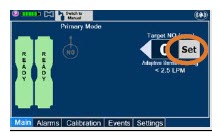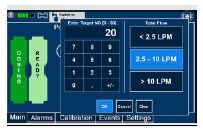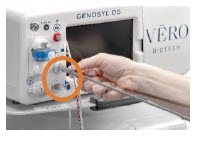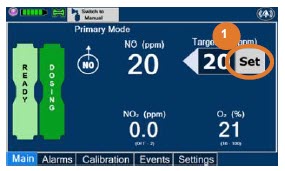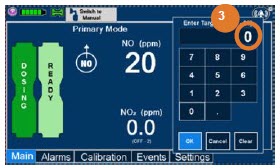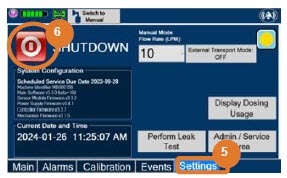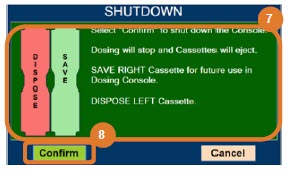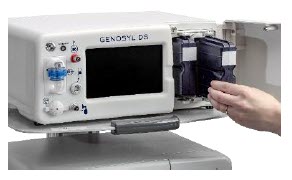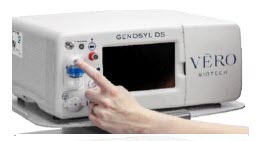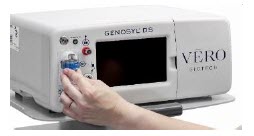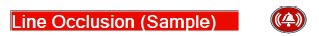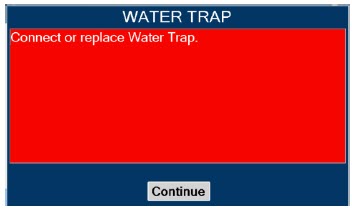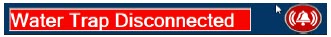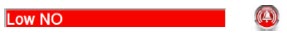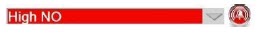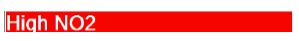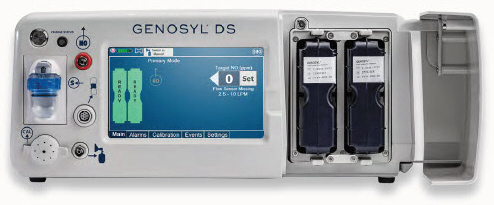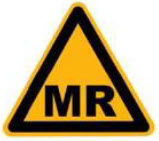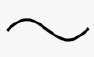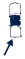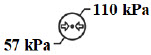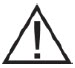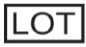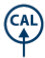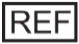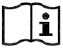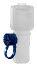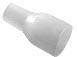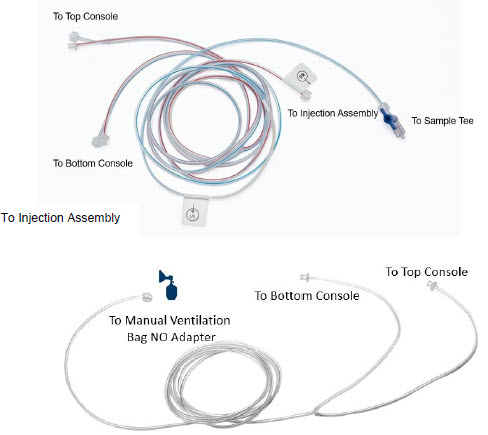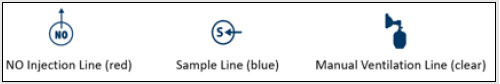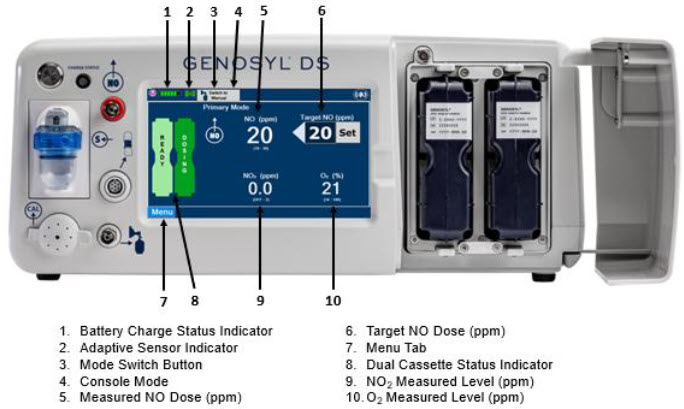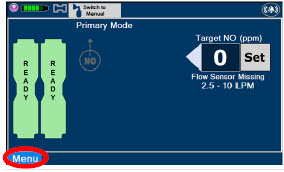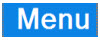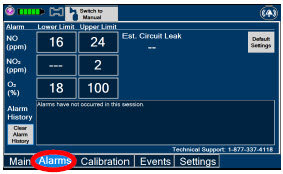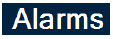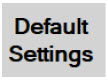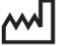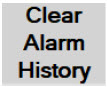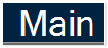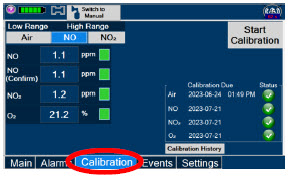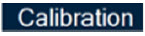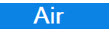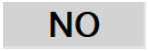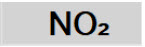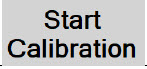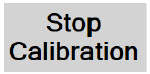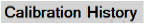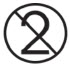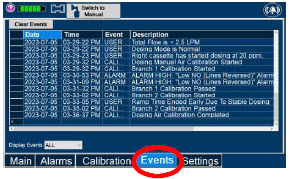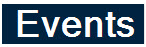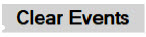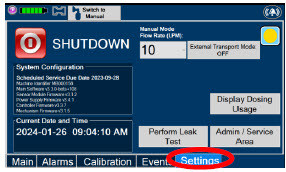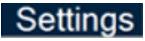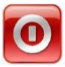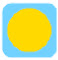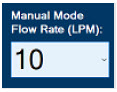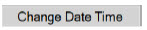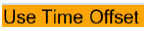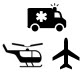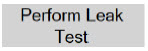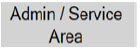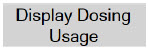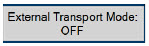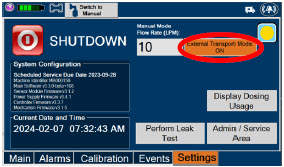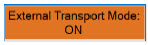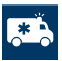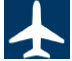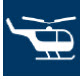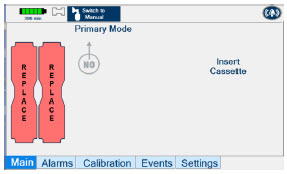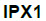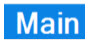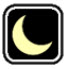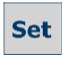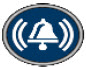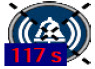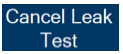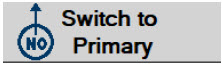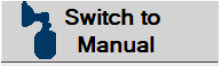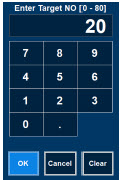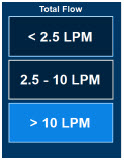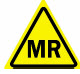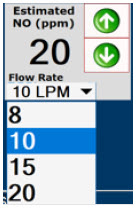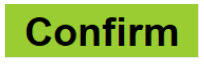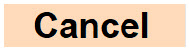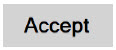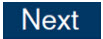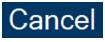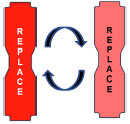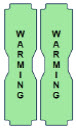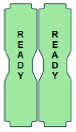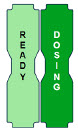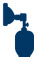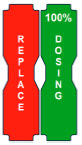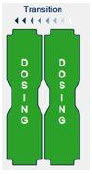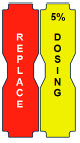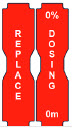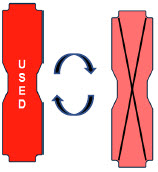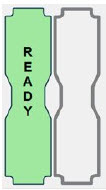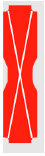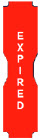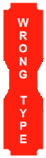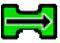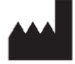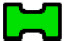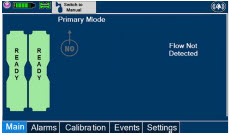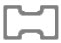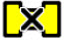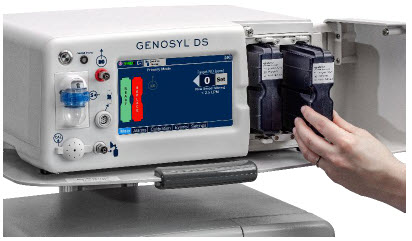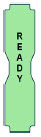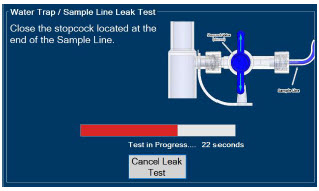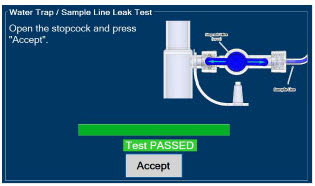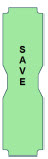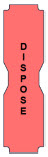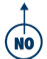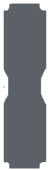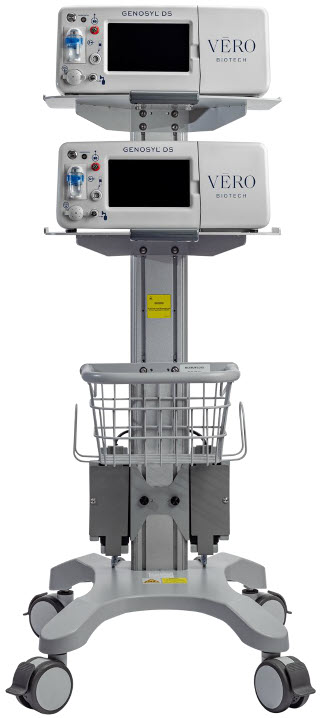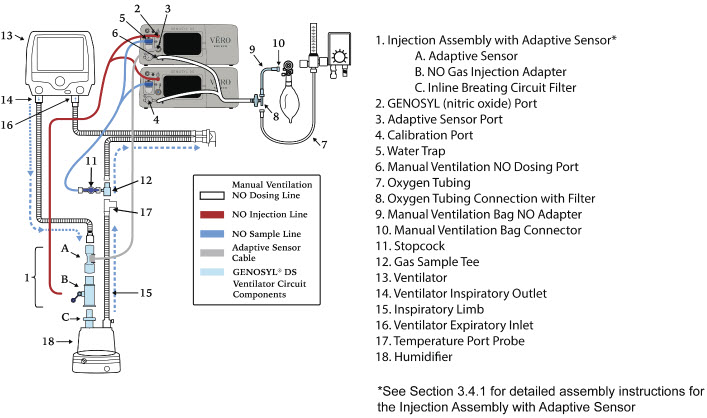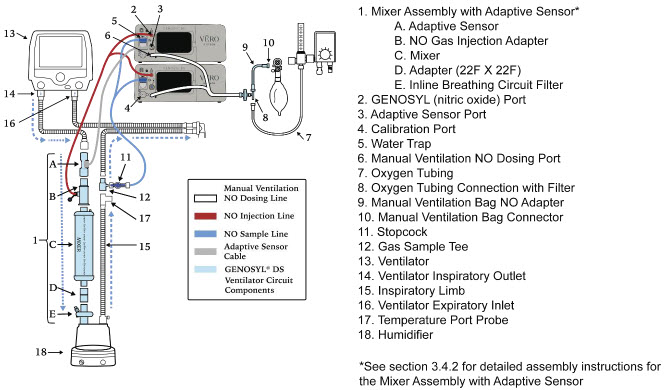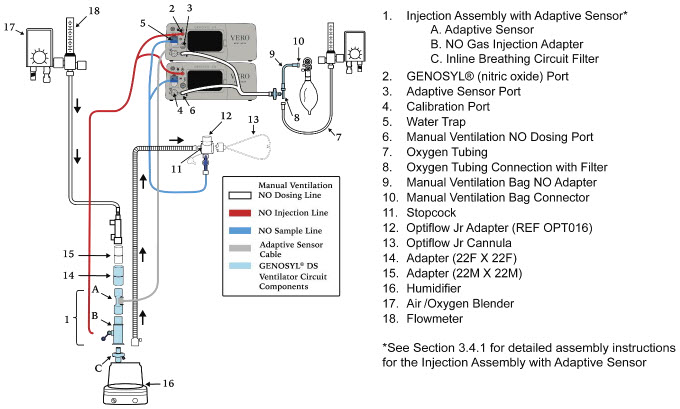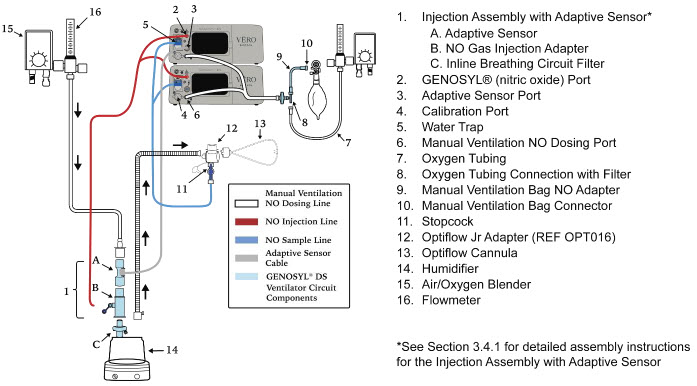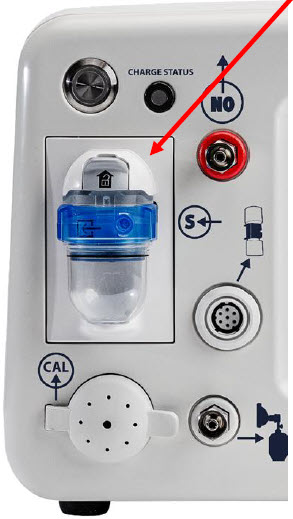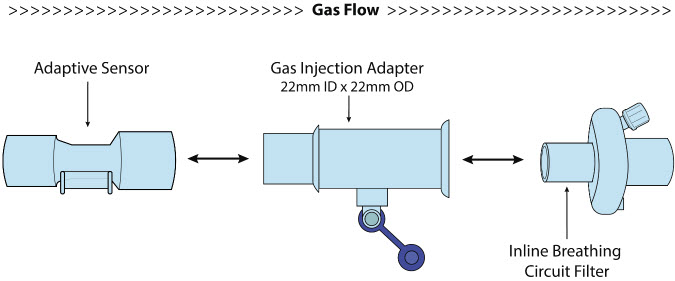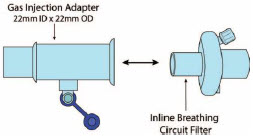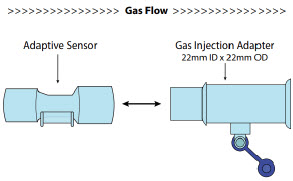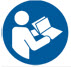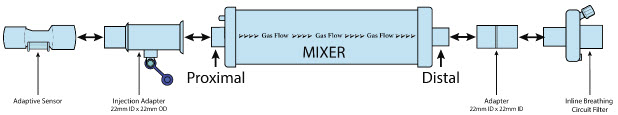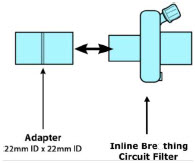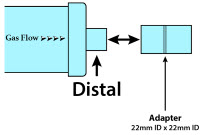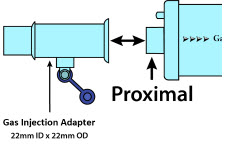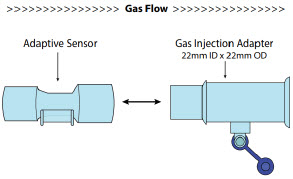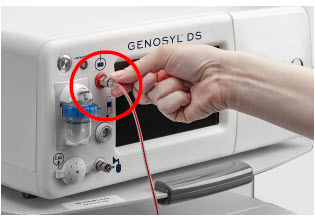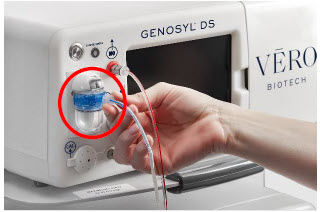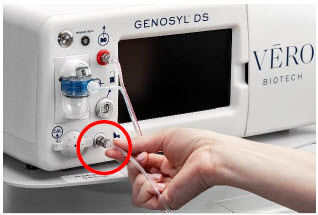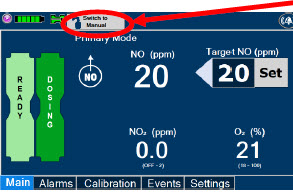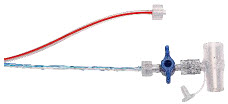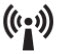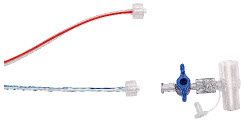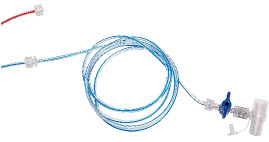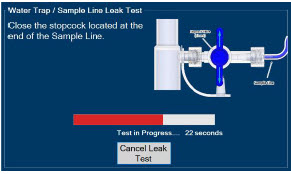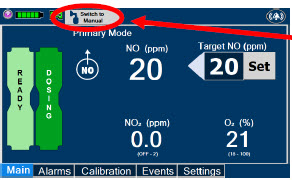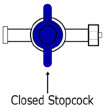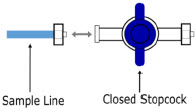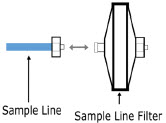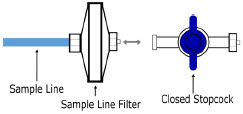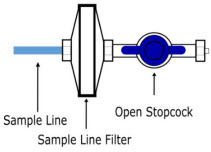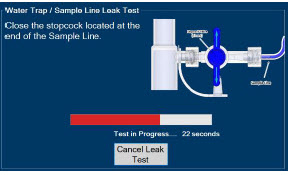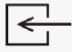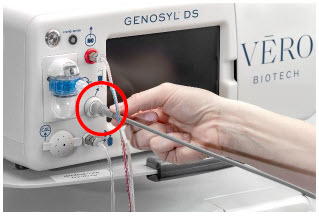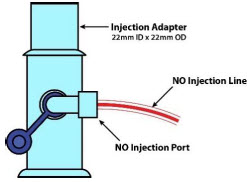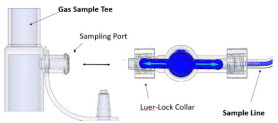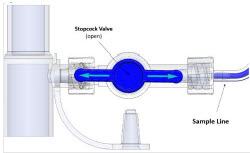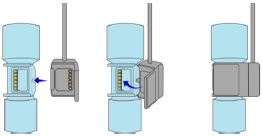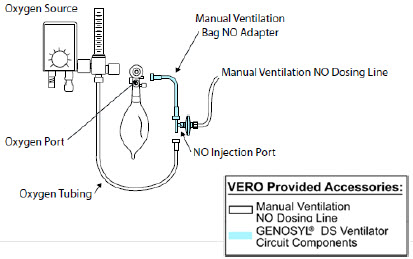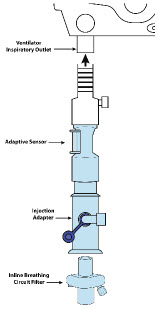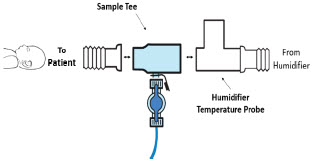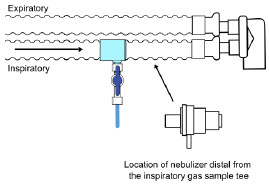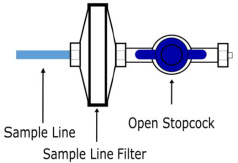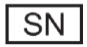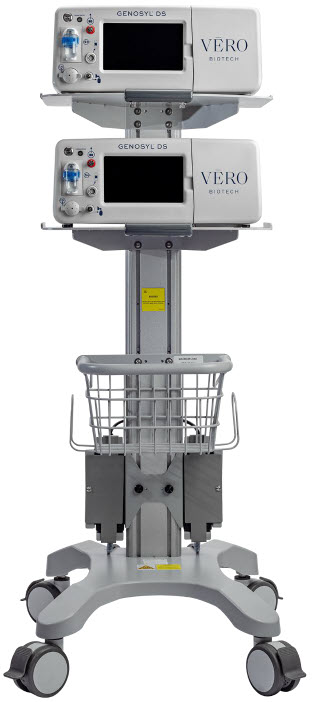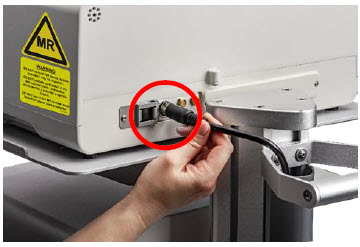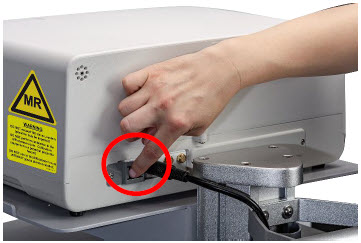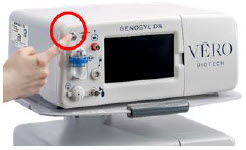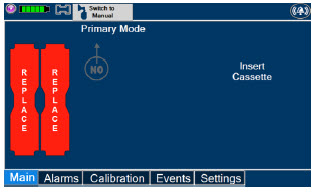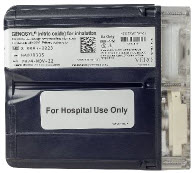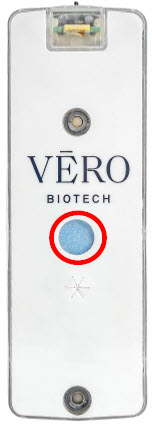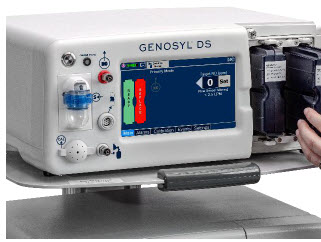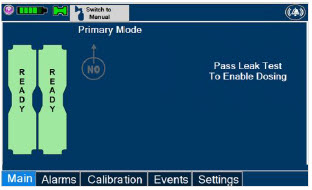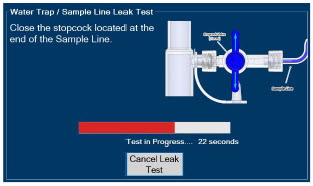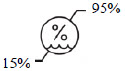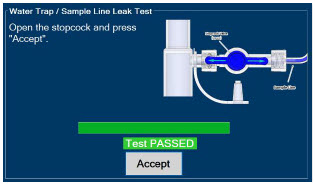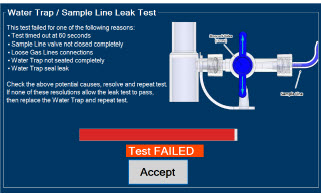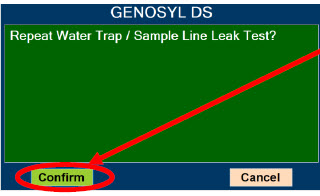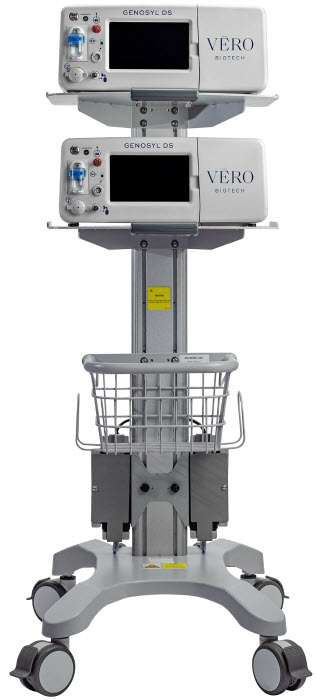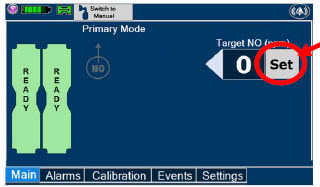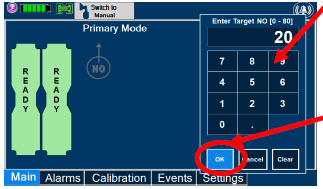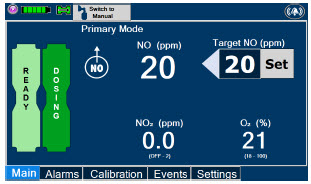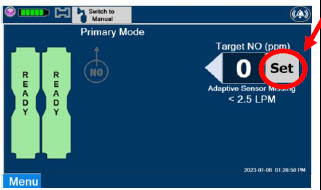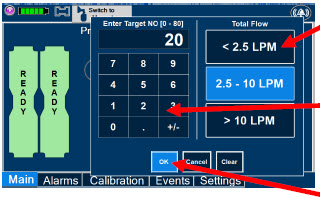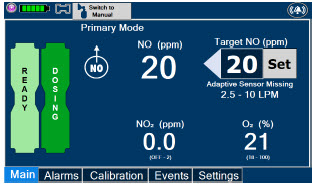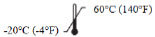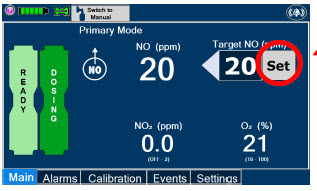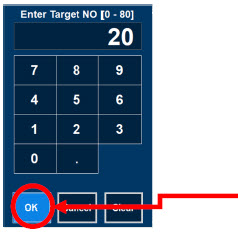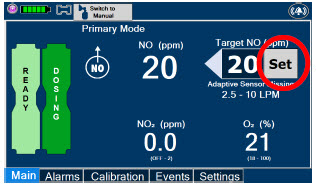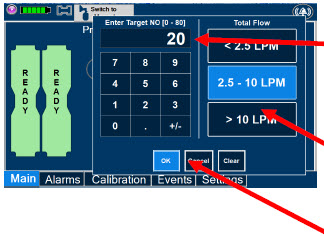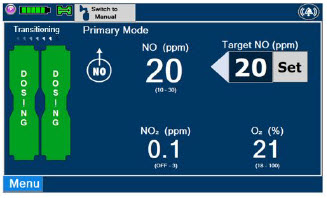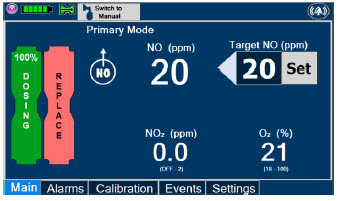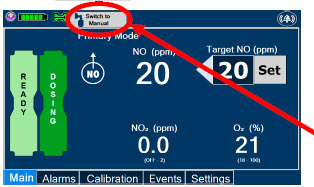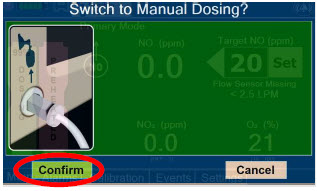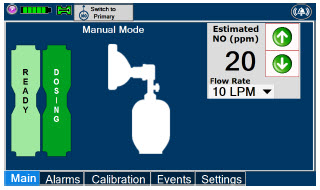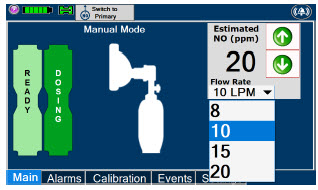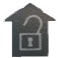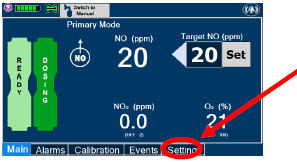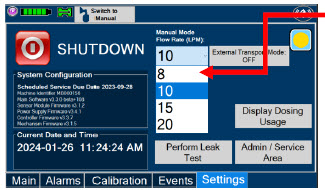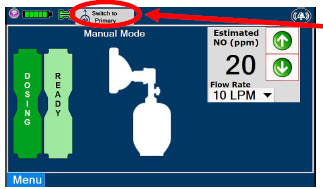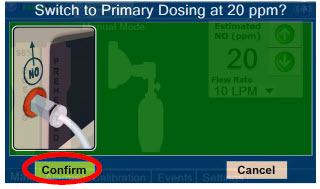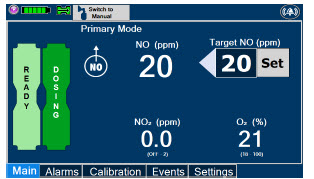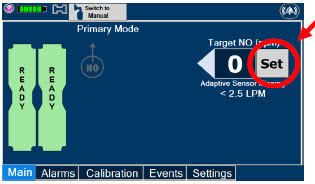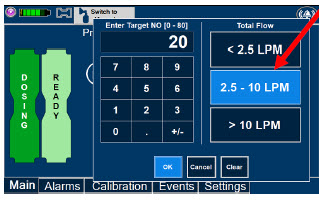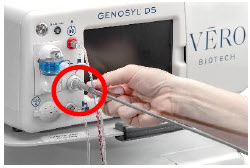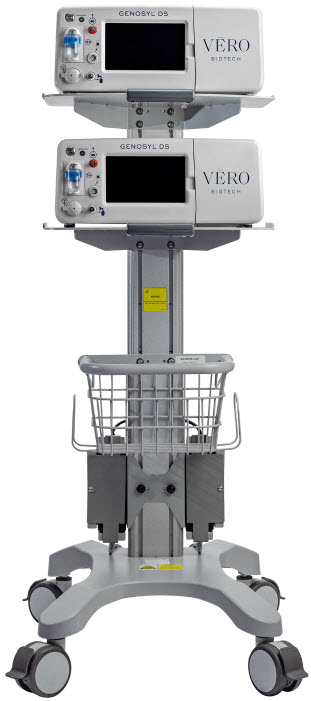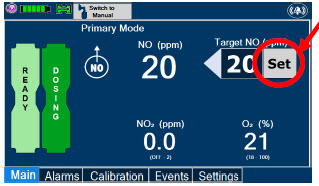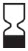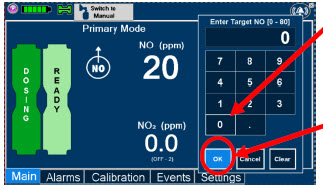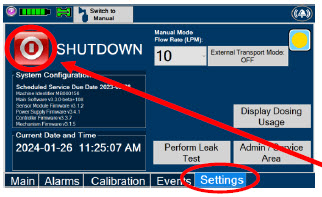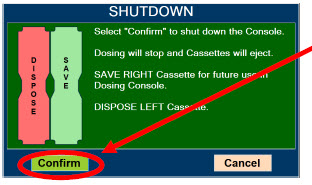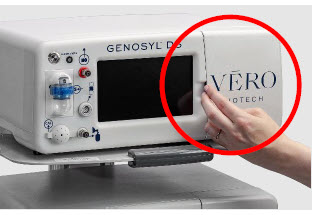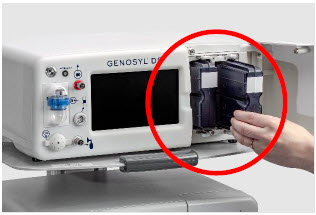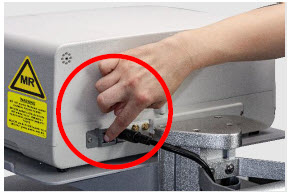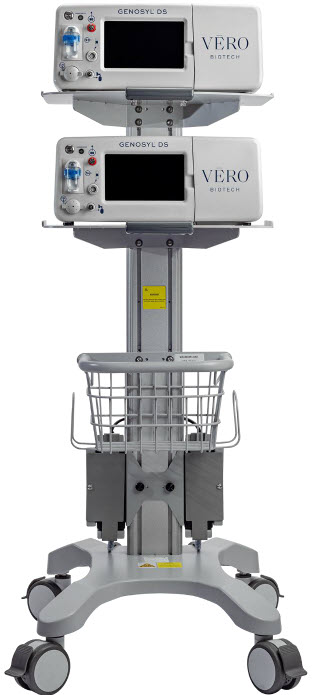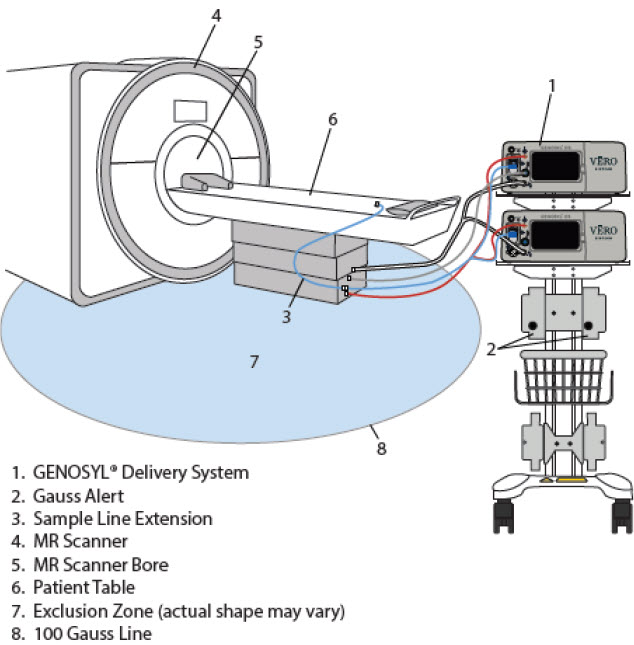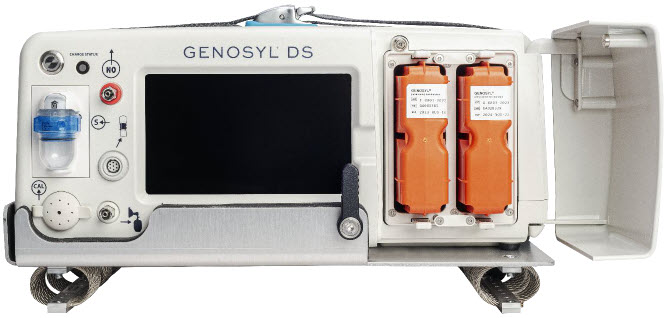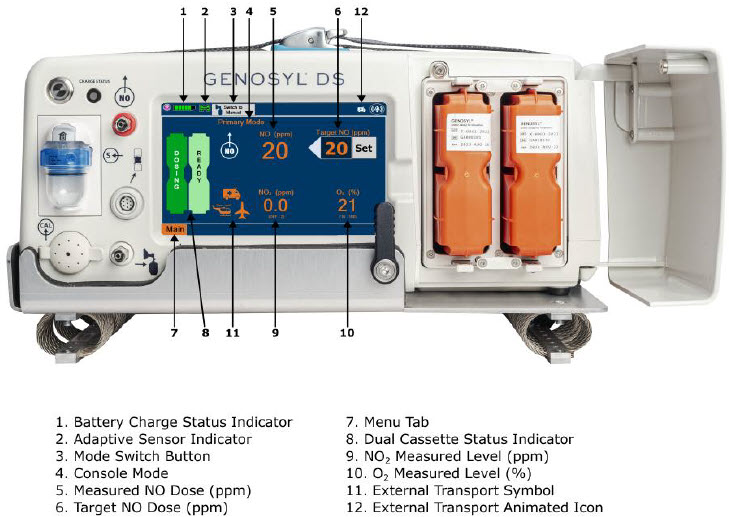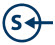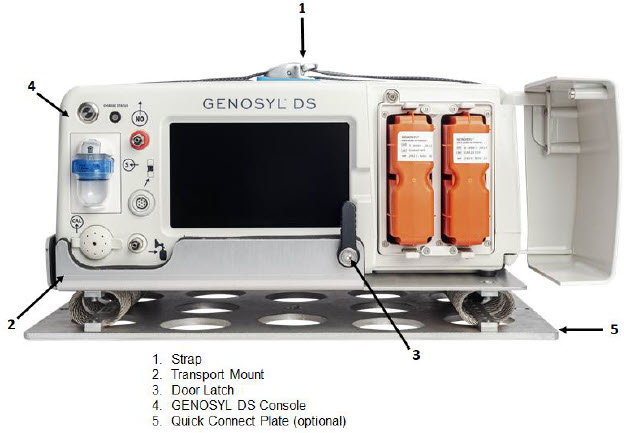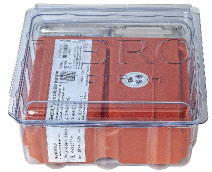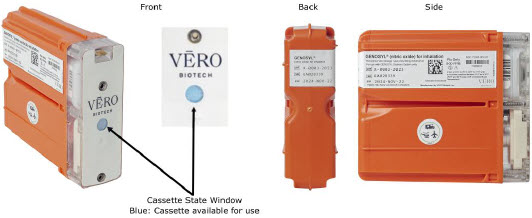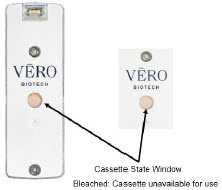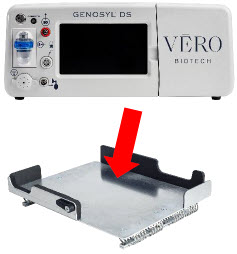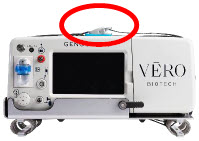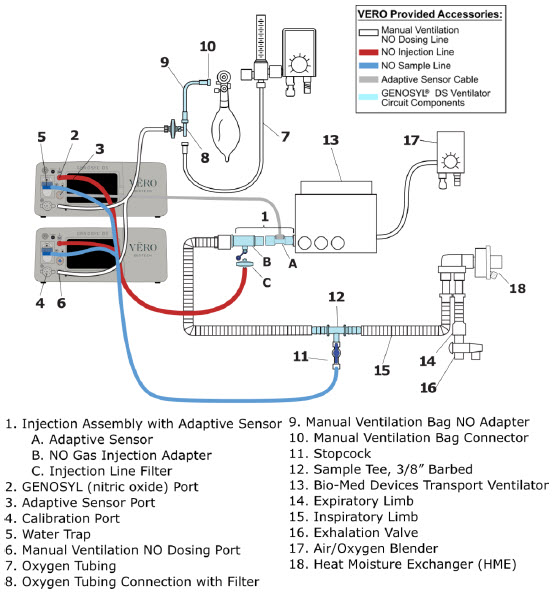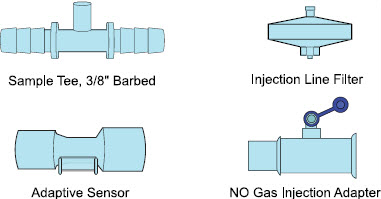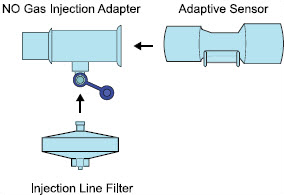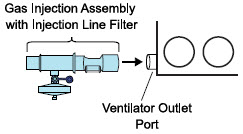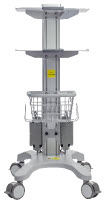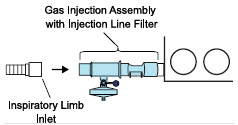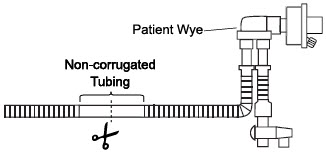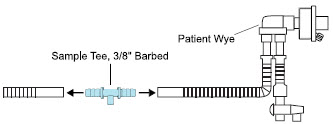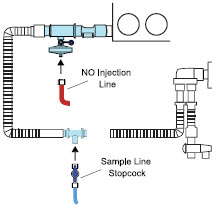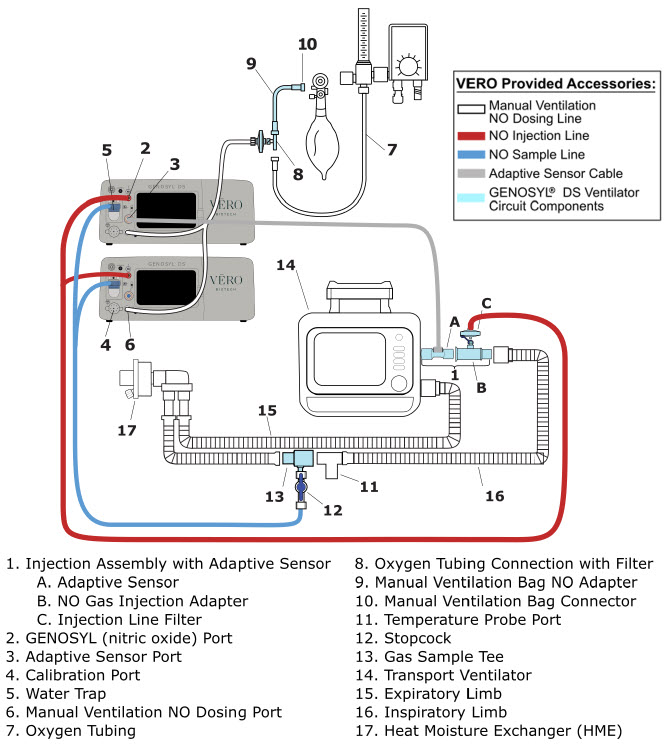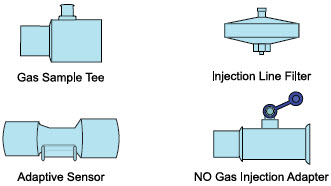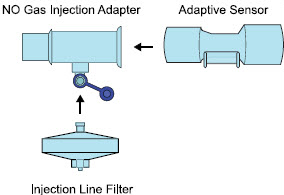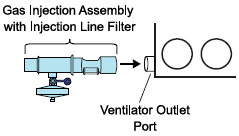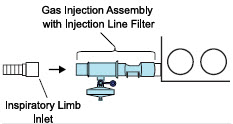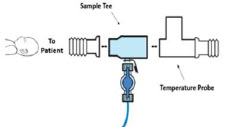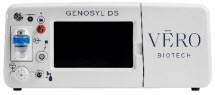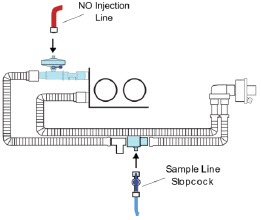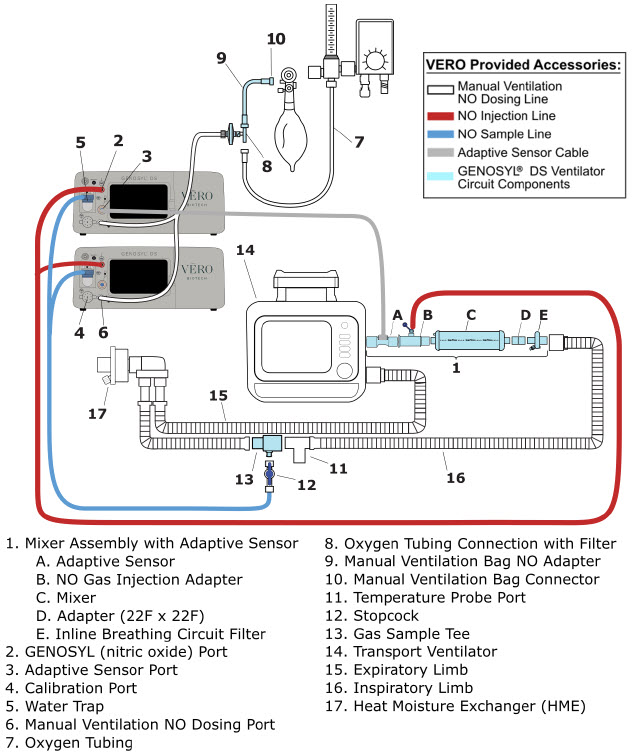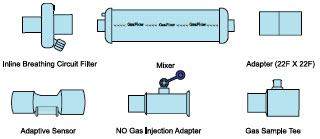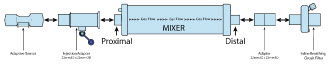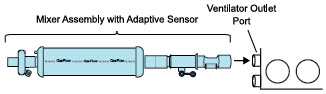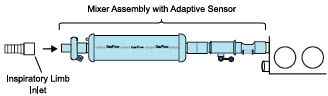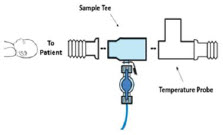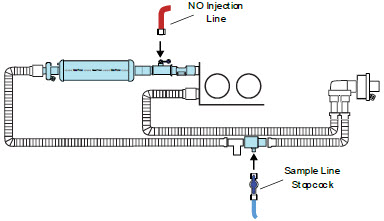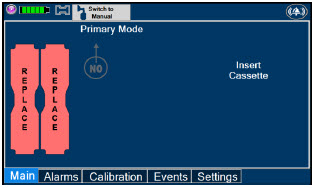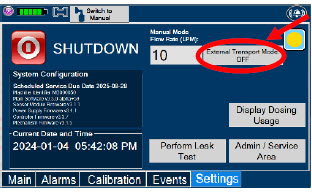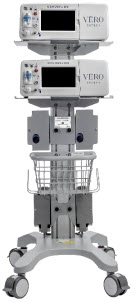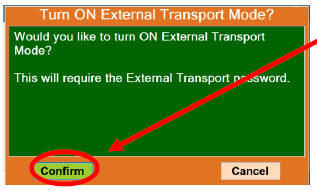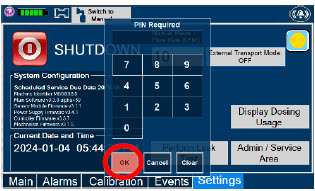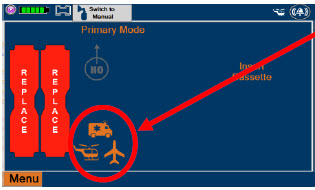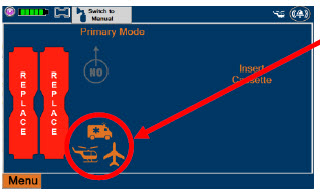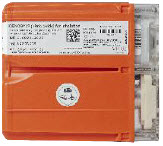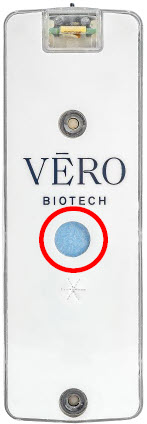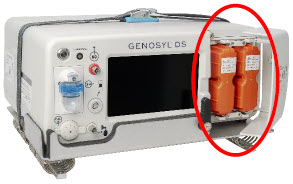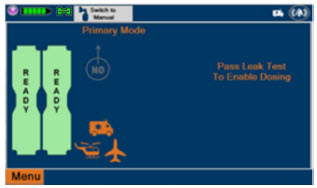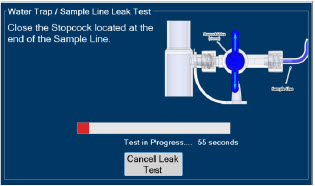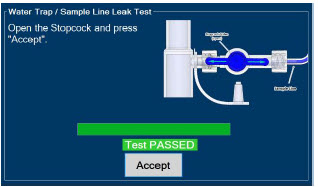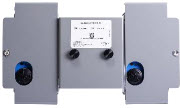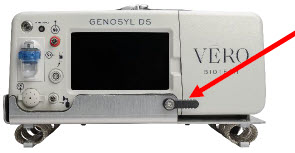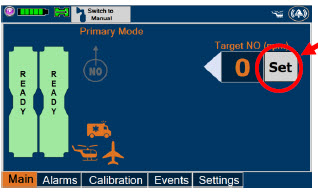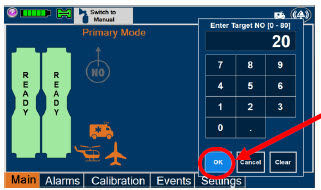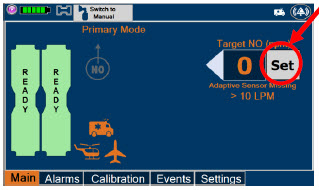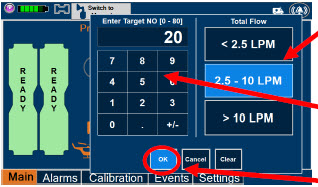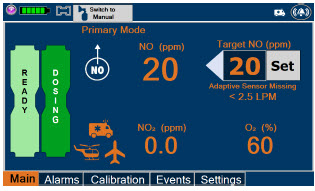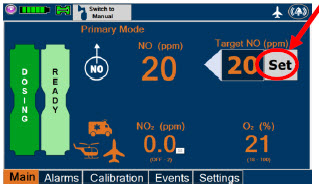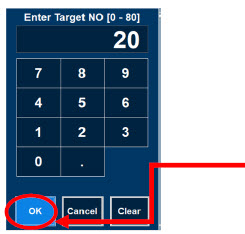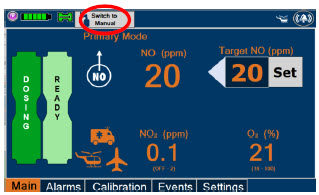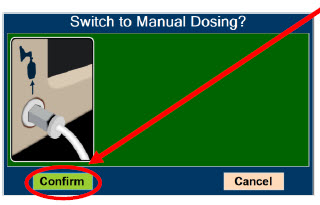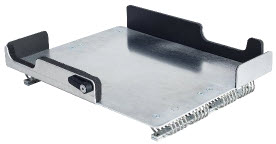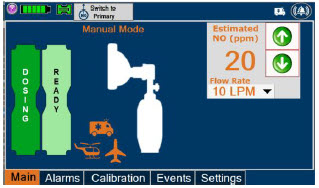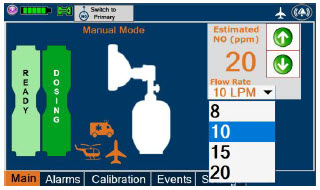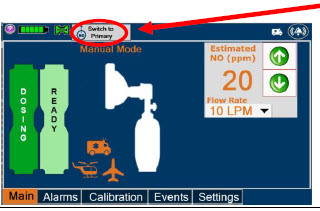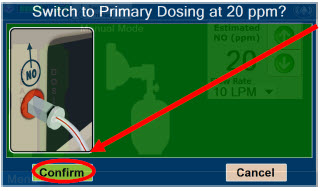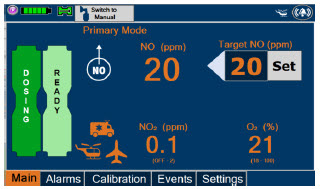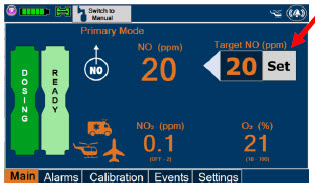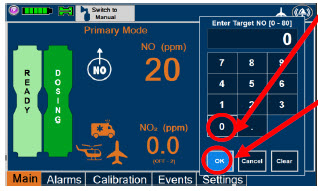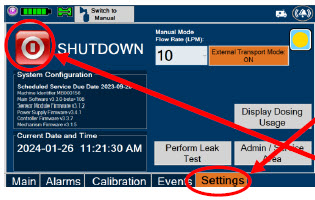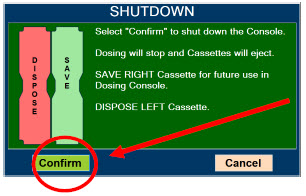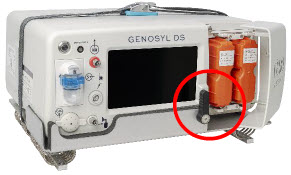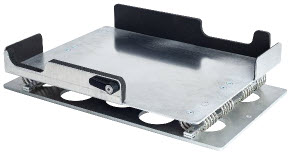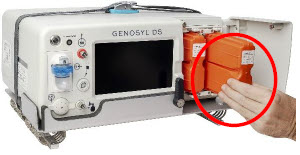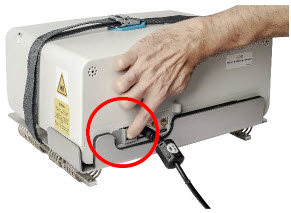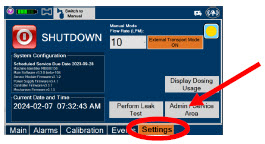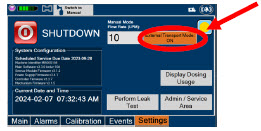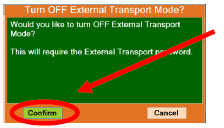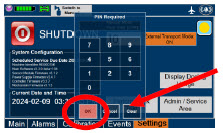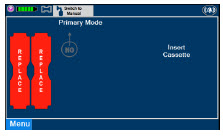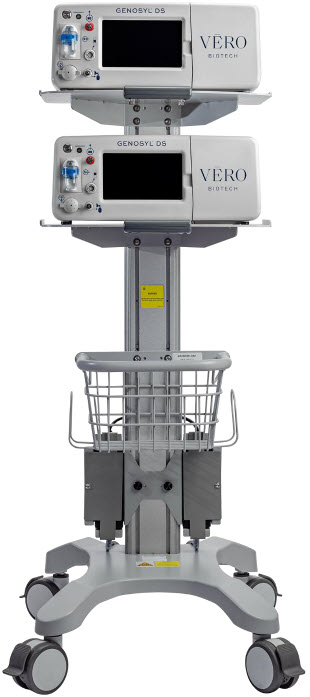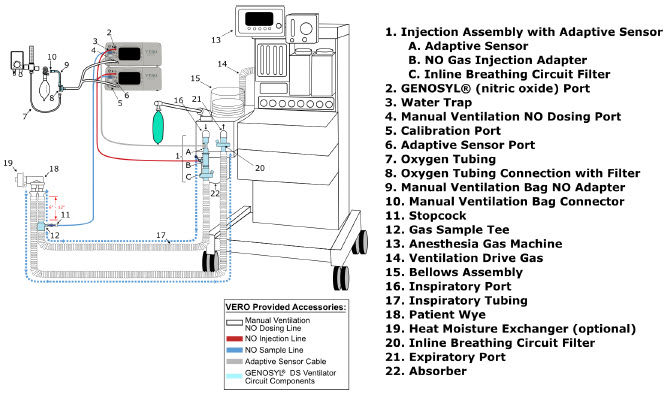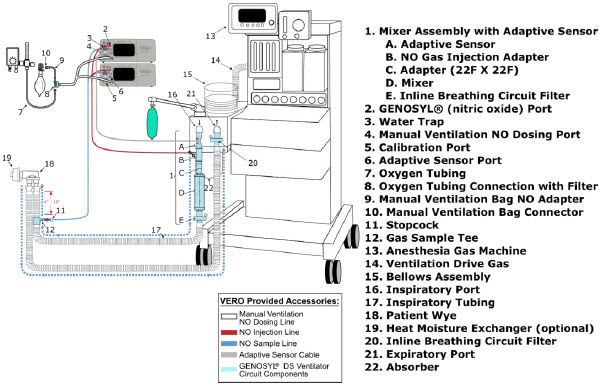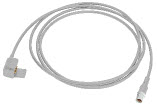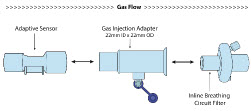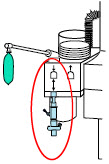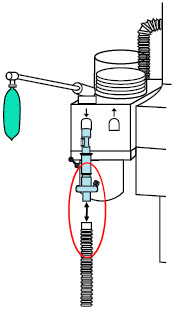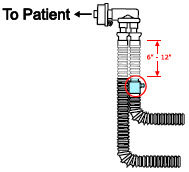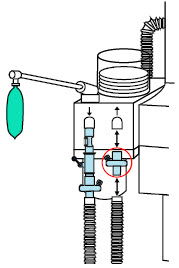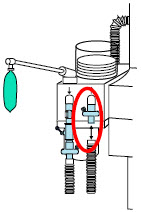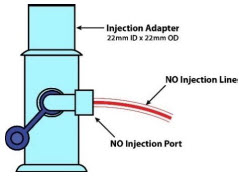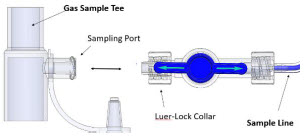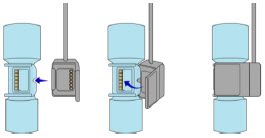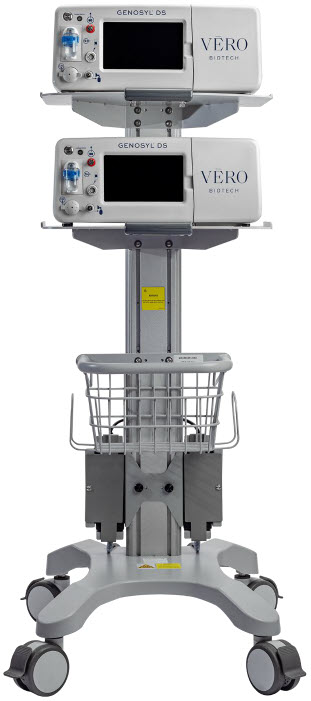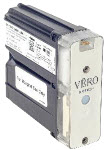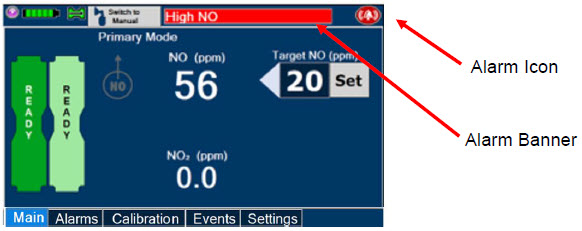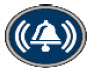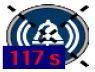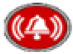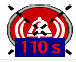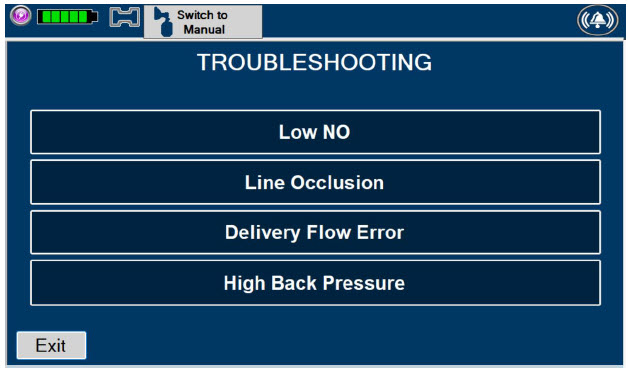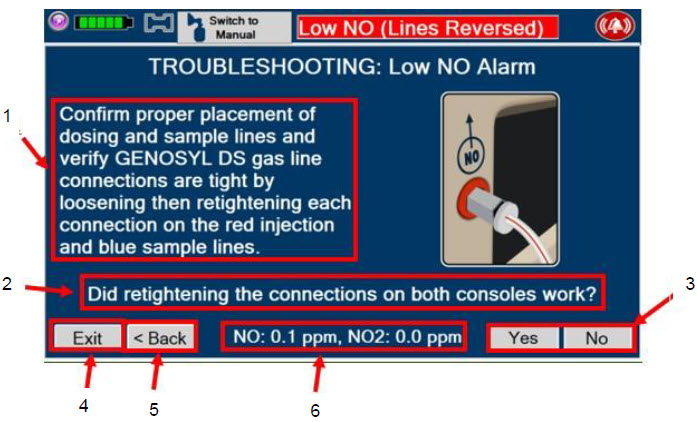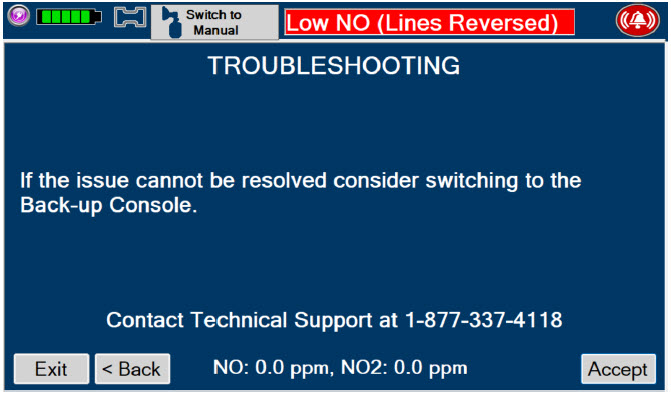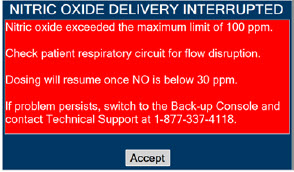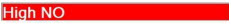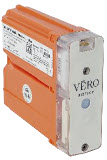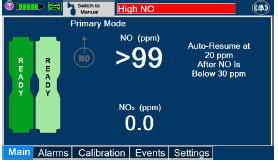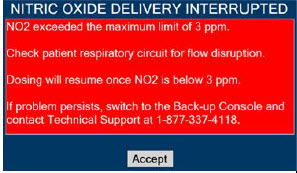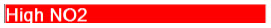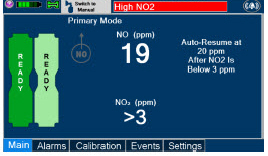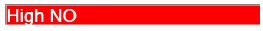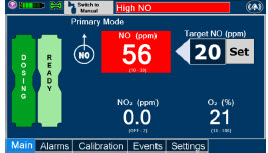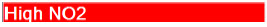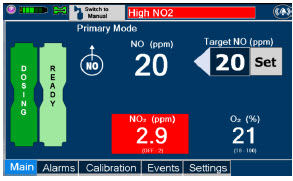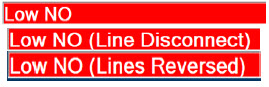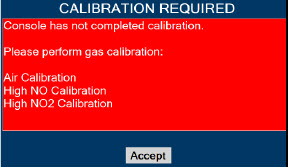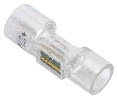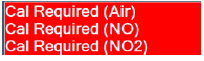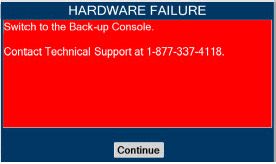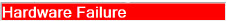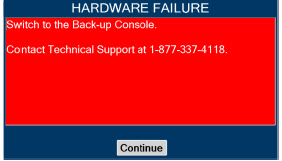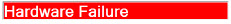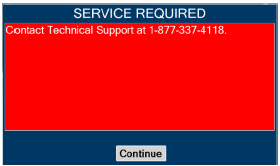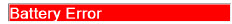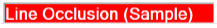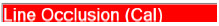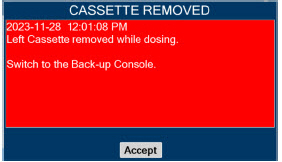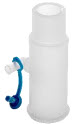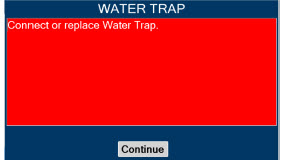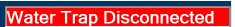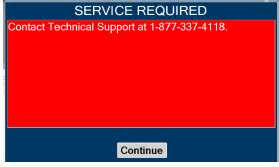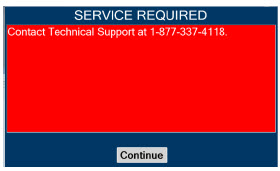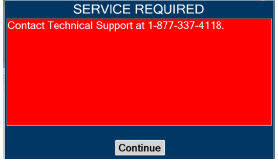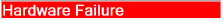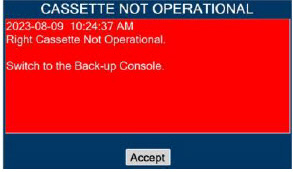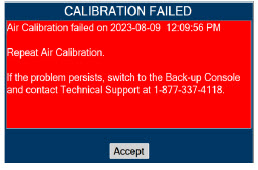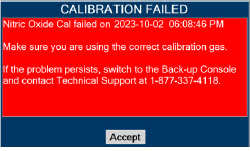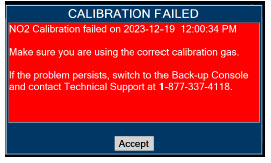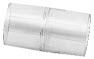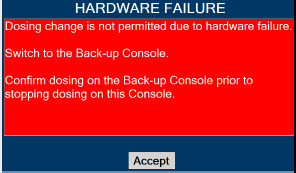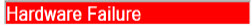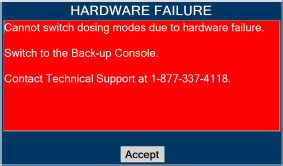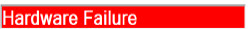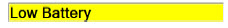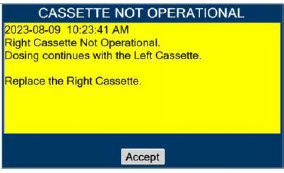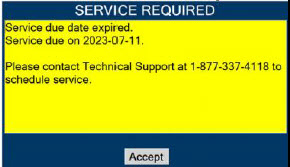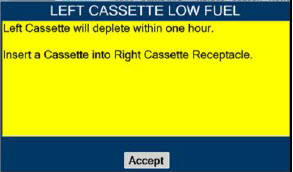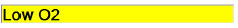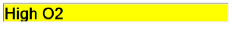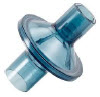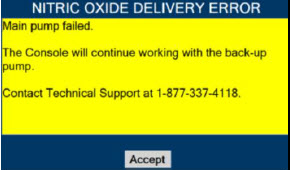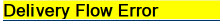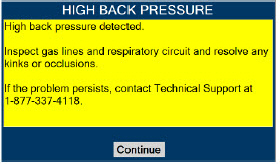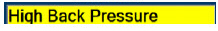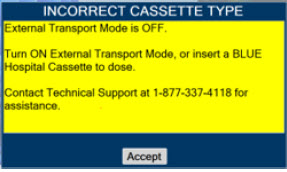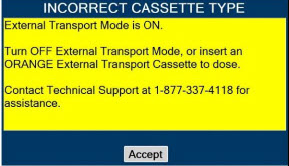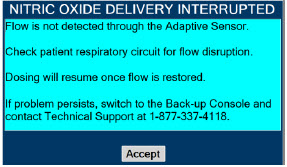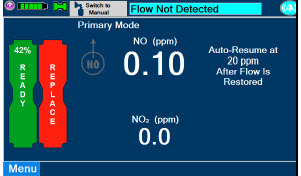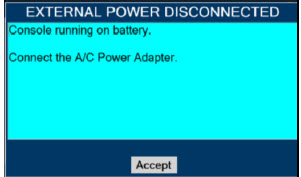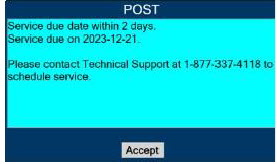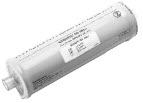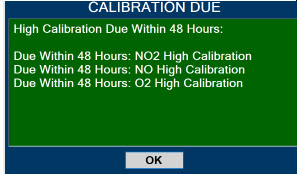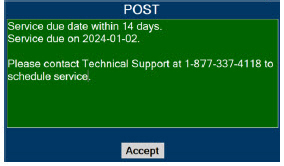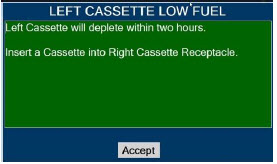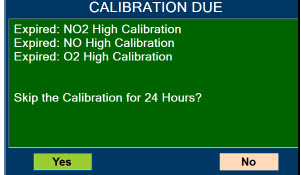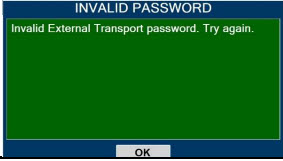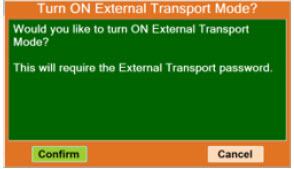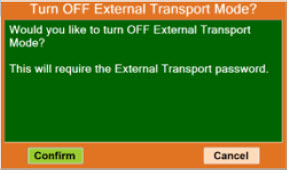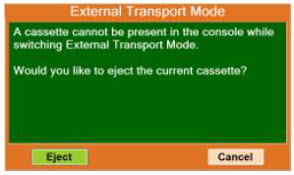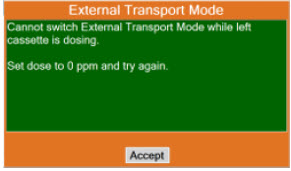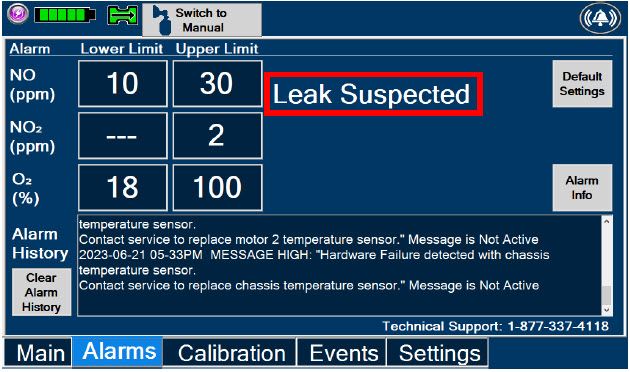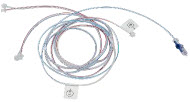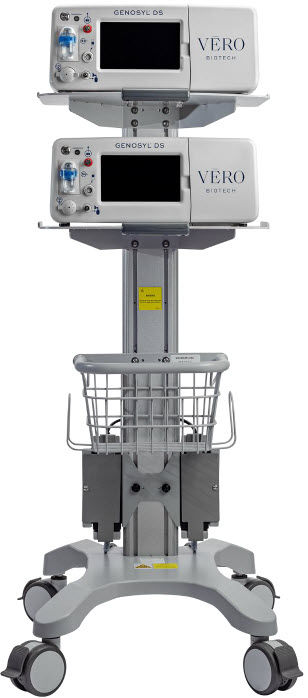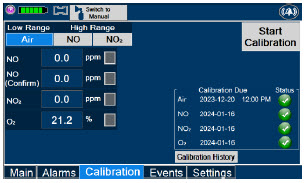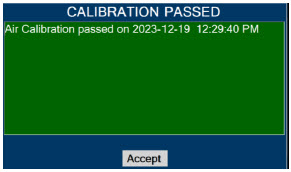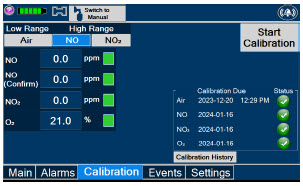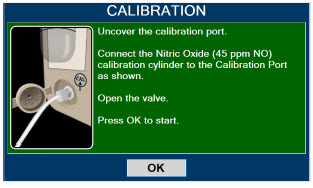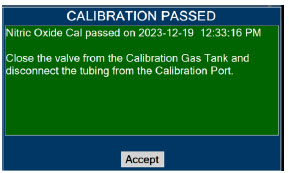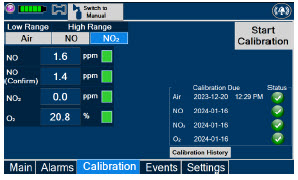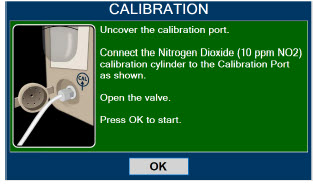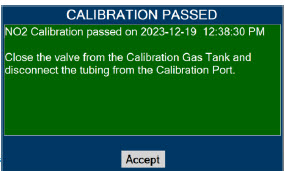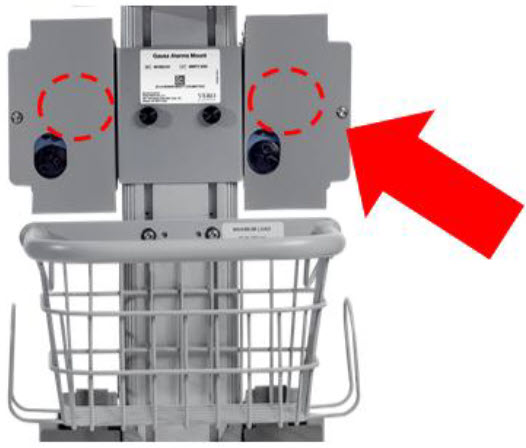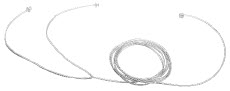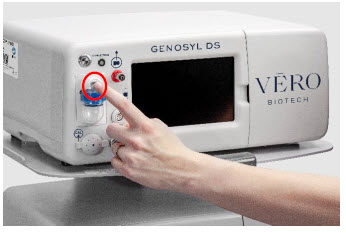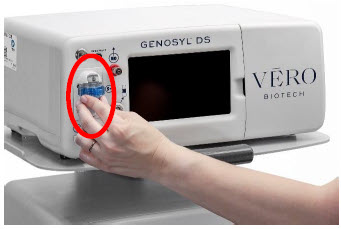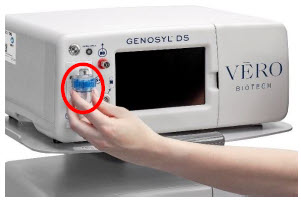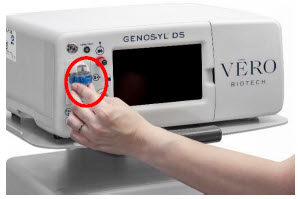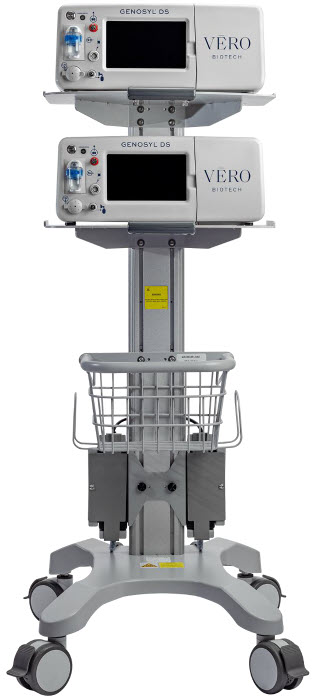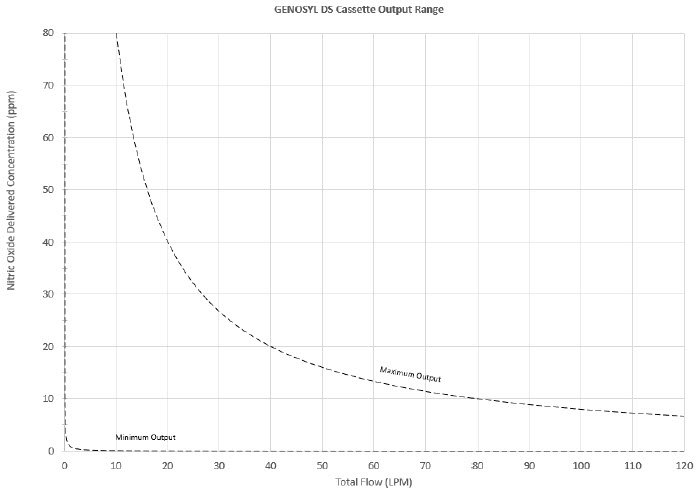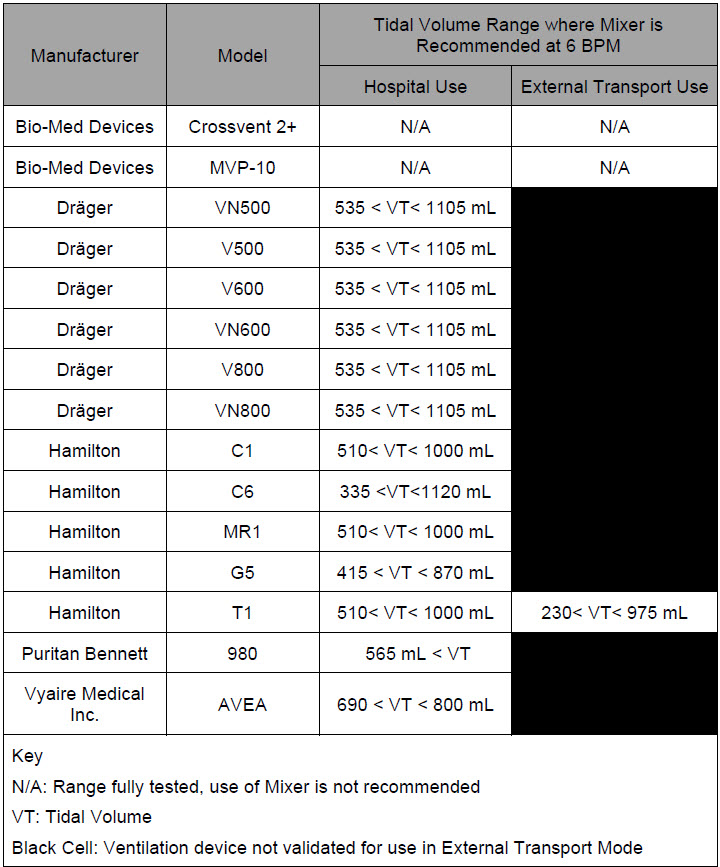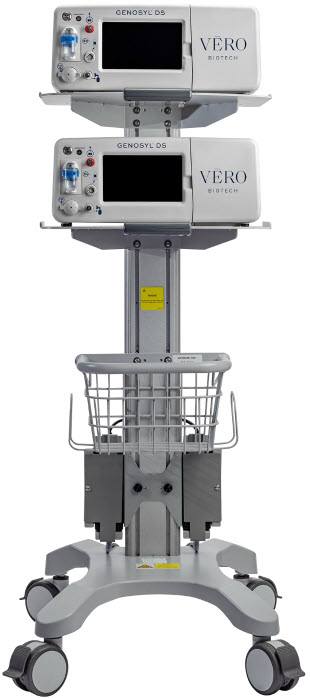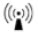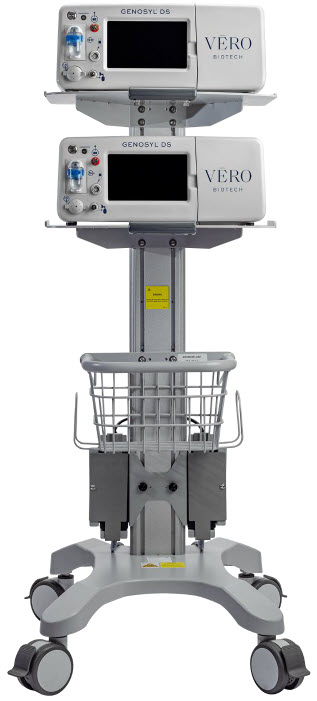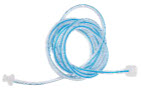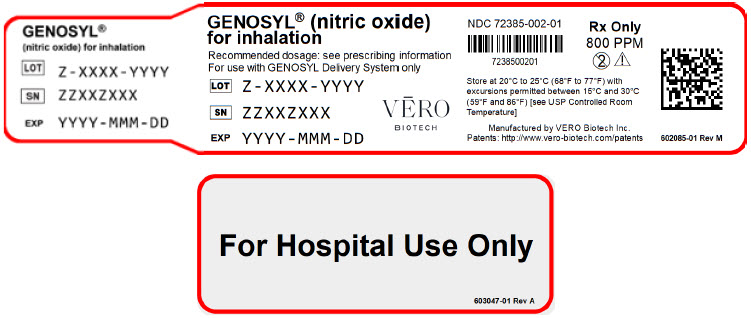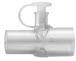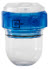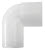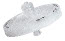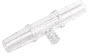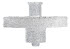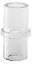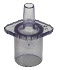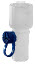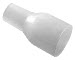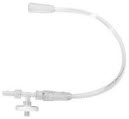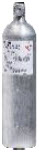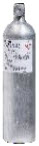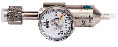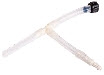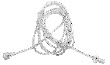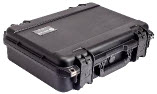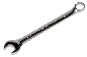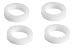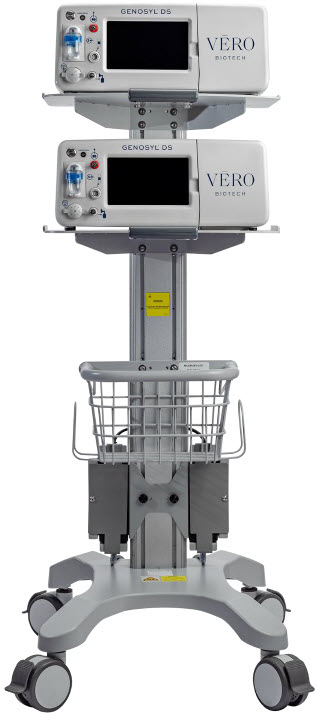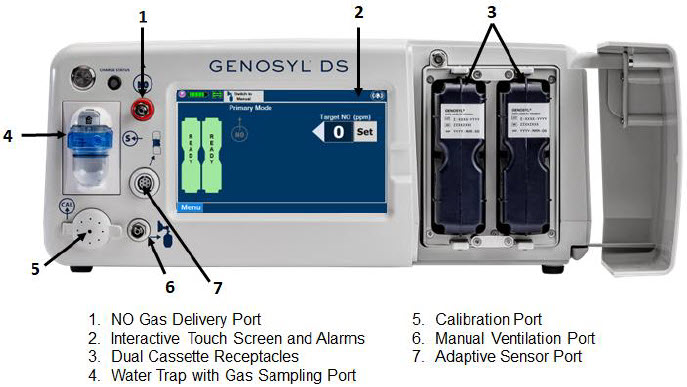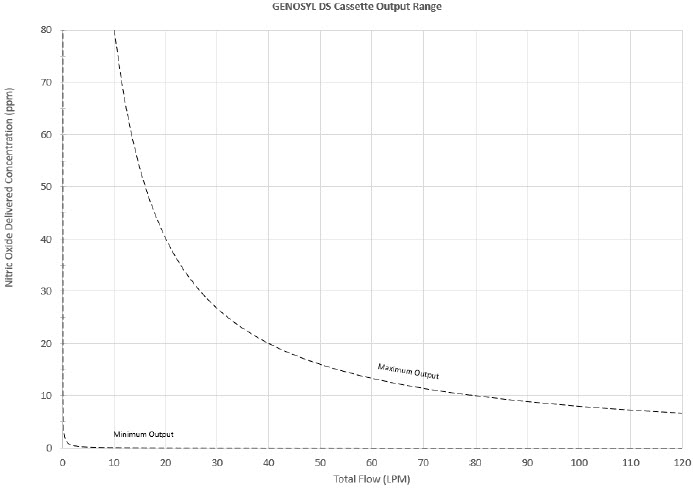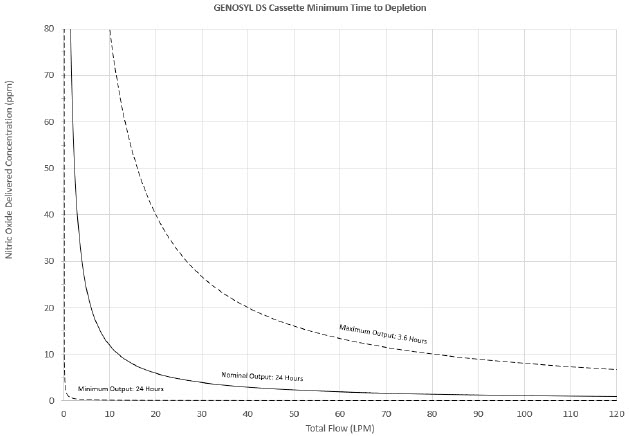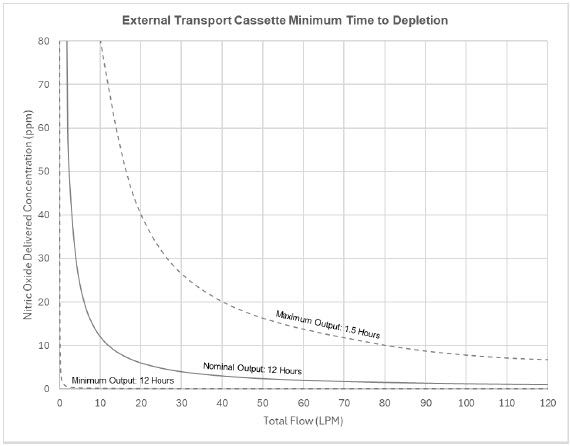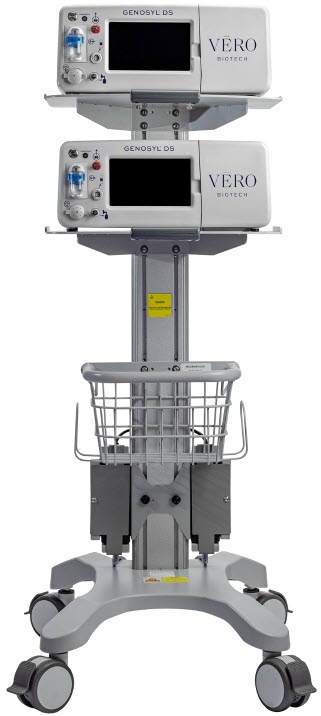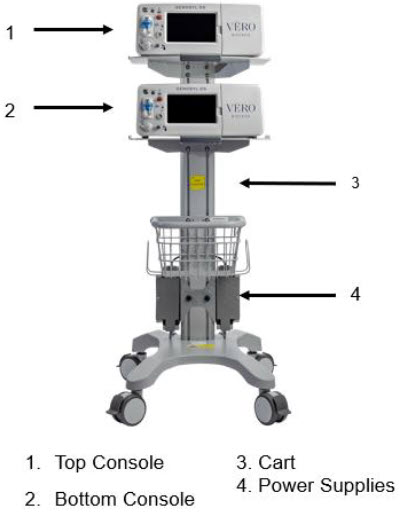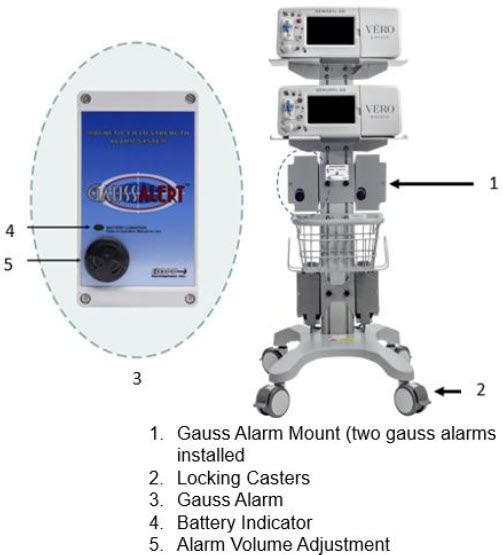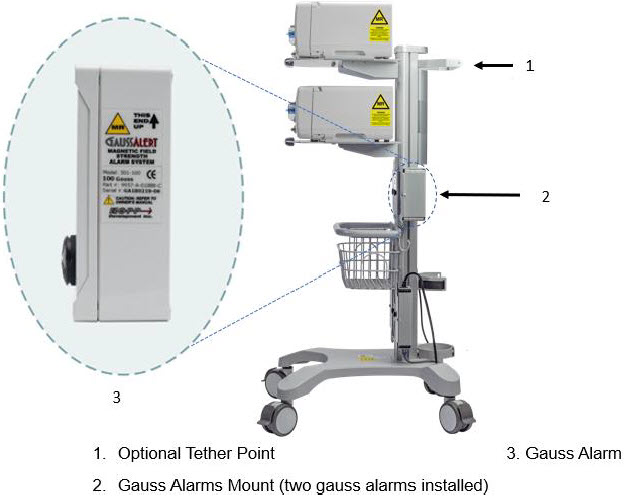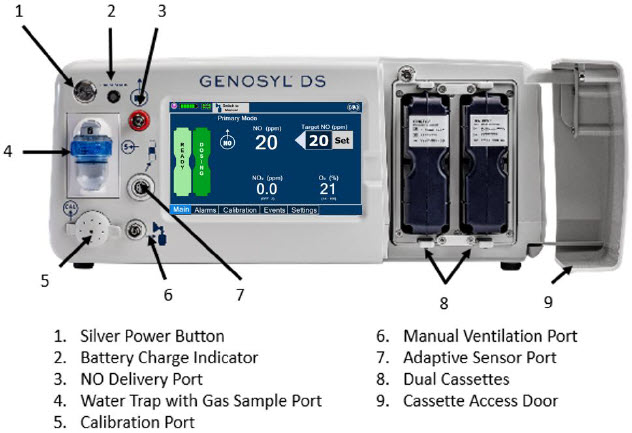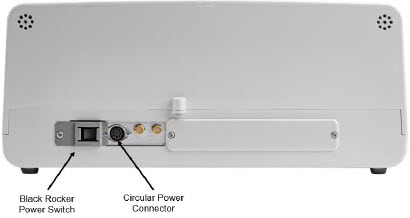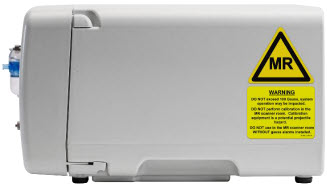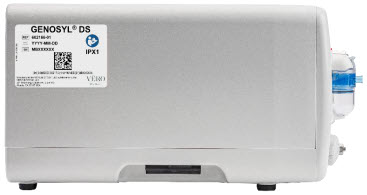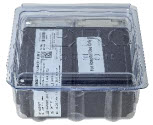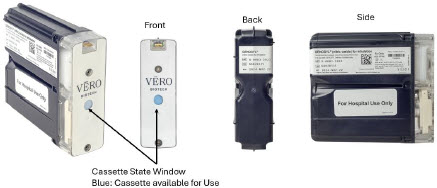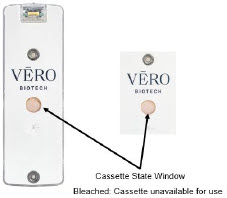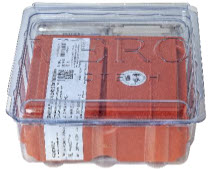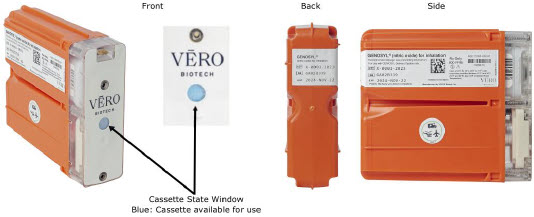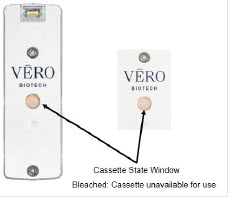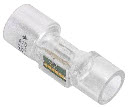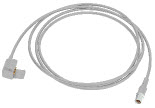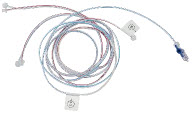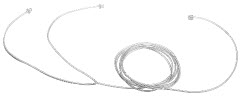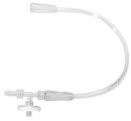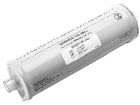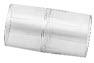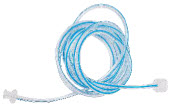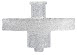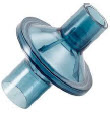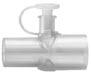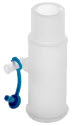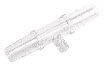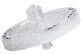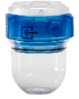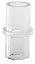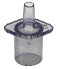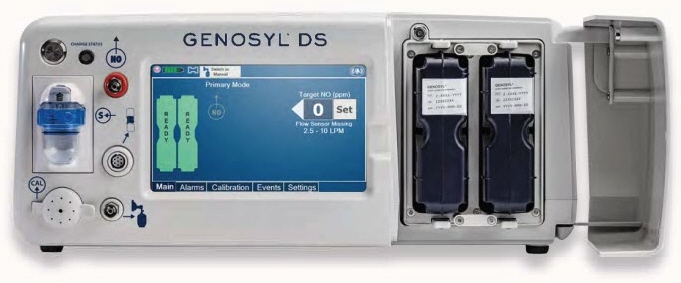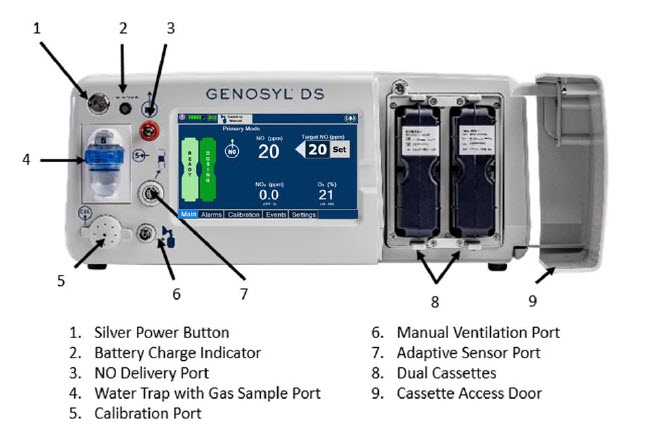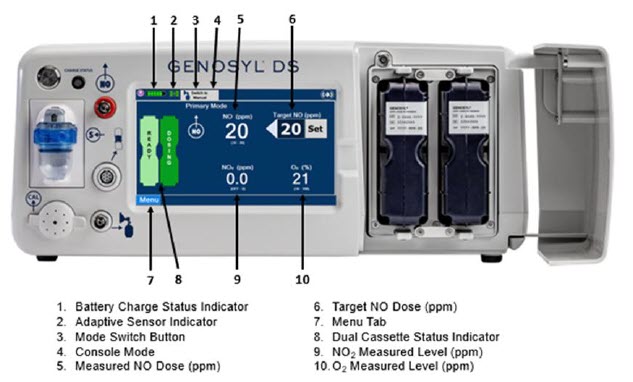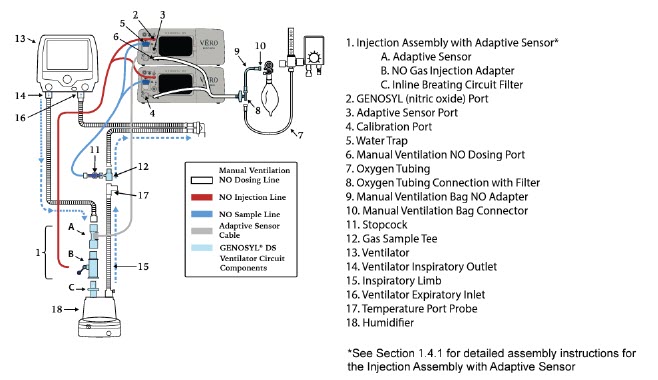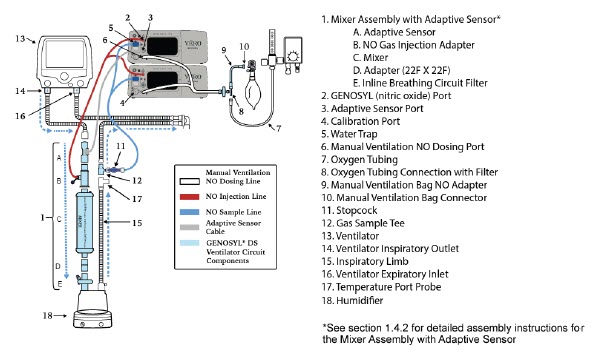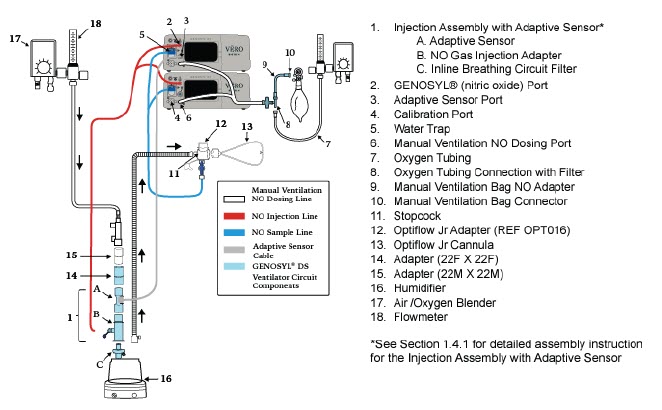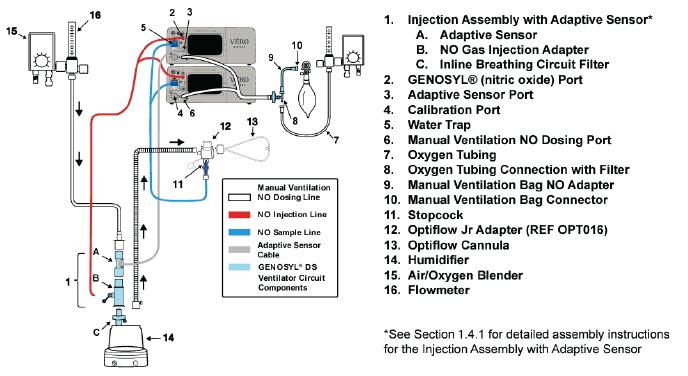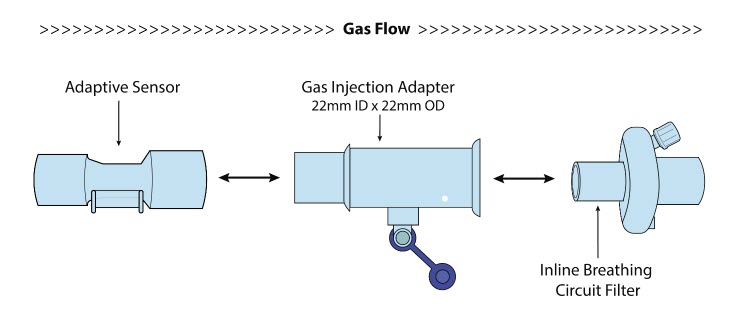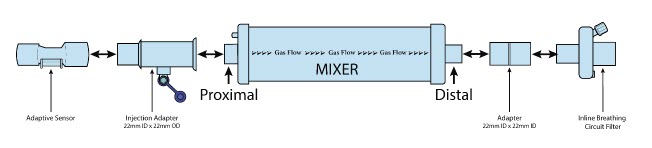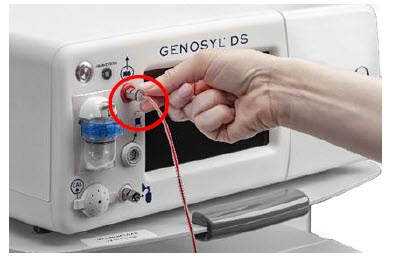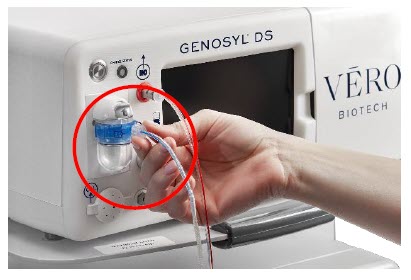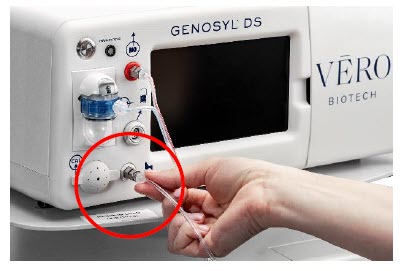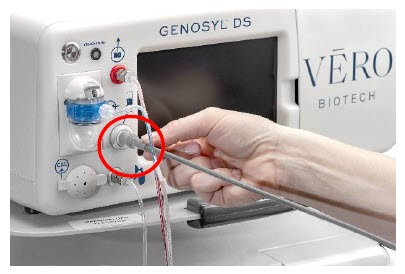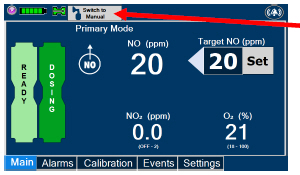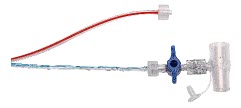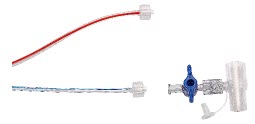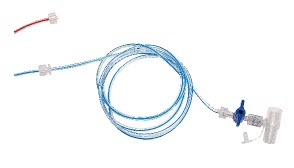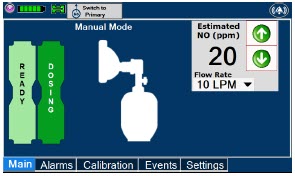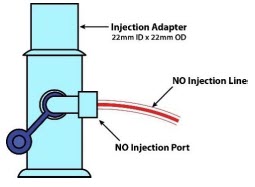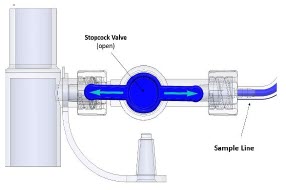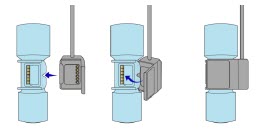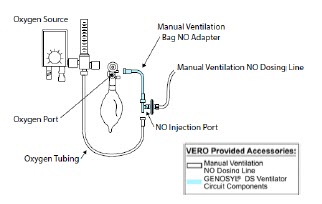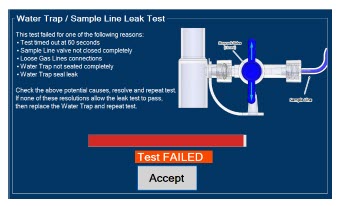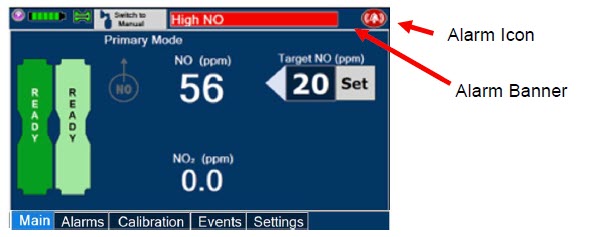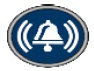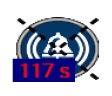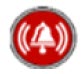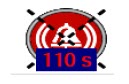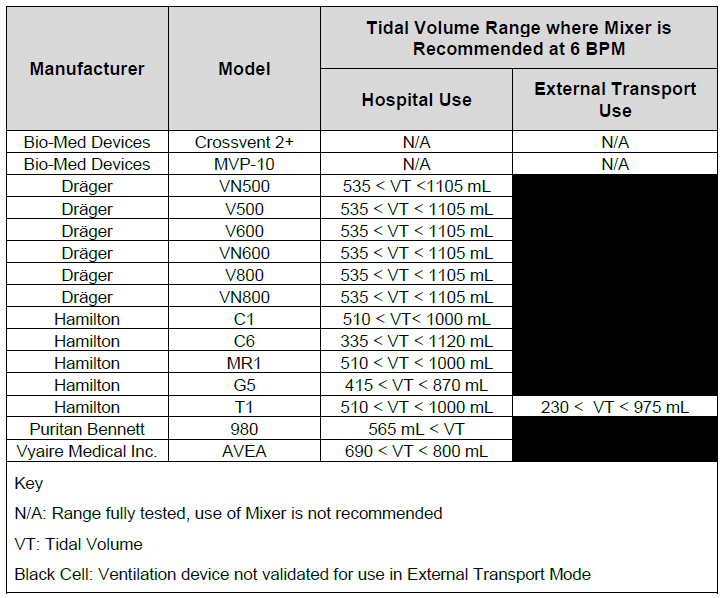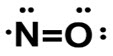 DRUG LABEL: GENOSYL
NDC: 72385-002 | Form: GAS
Manufacturer: VERO BIOTECH, INC.
Category: prescription | Type: HUMAN PRESCRIPTION DRUG LABEL
Date: 20251204

ACTIVE INGREDIENTS: NITRIC OXIDE 0.98 mg/1 L

HIGHLIGHTS OF PRESCRIBING INFORMATION

These highlights do not include all the information needed to use GENOSYL®safely and effectively. See full prescribing information for GENOSYL.
GENOSYL (nitric oxide), for inhalation use
Initial U.S. Approval: 1999

1 INDICATIONS AND USAGE

GENOSYL is a vasodilator indicated to improve oxygenation and reduce the need for extracorporeal membrane oxygenation in term and near-term (>34 weeks gestation) neonates with hypoxic respiratory failure associated with clinical or echocardiographic evidence of pulmonary hypertension in conjunction with ventilatory support and other appropriate agents (1).

2 DOSAGE AND ADMINISTRATION

The recommended dose is 20 ppm, maintained for up to 14 days or until the underlying oxygen desaturation has resolved (2.1).

Doses greater than 20 ppm are not recommended (2.1, 5.2).

Administration: Avoid abrupt discontinuation (2.2, 5.1).

3 DOSAGE FORMS AND STRENGTHS

GENOSYL (nitric oxide) is a gas, available at concentrations up to 800 ppm.

4 CONTRAINDICATIONS

Neonates dependent on right-to-left shunting of blood (4).

5 WARNINGS AND PRECAUTIONS

Rebound Pulmonary Hypertension: Abrupt discontinuation of GENOSYL may lead to worsening oxygenation and increasing pulmonary artery pressure (5.1).

Methemoglobinemia: Methemoglobin increases with the dose of nitric oxide; following discontinuation or reduction of nitric oxide, methemoglobin levels return to baseline over a period of hours (5.2).

Elevated NO2Levels: Monitor NO2levels (5.3).

Heart Failure: In patients with pre-existing left ventricular dysfunction, GENOSYL may increase pulmonary capillary wedge pressure leading to pulmonary edema (5.4).

6 ADVERSE REACTIONS

The most common adverse reaction is hypotension (6).

To report SUSPECTED ADVERSE REACTIONS, contact Vero Biotech at 1-877-337-4118 and http://www.vero-biotech.com/ or FDA at 1-800-FDA-1088 or www.fda.gov/medwatch.

7 DRUG INTERACTIONS

Nitric oxide donor compounds may increase the risk of developing methemoglobinemia (7).

FULL PRESCRIBING INFORMATION

1 INDICATIONS AND USAGE

GENOSYL®is indicated to improve oxygenation and reduce the need for extracorporeal membrane oxygenation in term and near-term (>34 weeks gestation) neonates with hypoxic respiratory failure associated with clinical or echocardiographic evidence of pulmonary hypertension in conjunction with ventilatory support and other appropriate agents.

2 DOSAGE AND ADMINISTRATION

2.1 Dosage

Term and near-term neonates with hypoxic respiratory failure

The recommended dose of GENOSYL is 20 ppm. Maintain treatment up to 14 days or until the underlying oxygen desaturation has resolved and the neonate is ready to be weaned from GENOSYL therapy.

Doses greater than 20 ppm are not recommended [see Warnings and Precautions (5.2)].

2.2 Administration

Nitric Oxide Delivery System

GENOSYL must be administered using a calibrated GENOSYL Delivery System. Only validated ventilator systems should be used in conjunction with GENOSYL [see Description (11)].

Consult the GENOSYL Delivery System Operator's Manual or call 1-877-337-4118 or visit www.vero-biotech.com for needed information on training and technical support for users of GENOSYL with the GENOSYL Delivery System .

Keep available a backup power supply to address power failures. The GENOSYL Delivery System consists of a primary system and a fully functional second system that can be used as backup in the event of primary system failure.

Monitoring

Measure methemoglobin within 4-8 hours after initiation of treatment with GENOSYL and periodically throughout treatment [see Warnings and Precautions (5.2)].

Monitor for PaO2and inspired NO2during GENOSYL administration [see Warnings and Precautions 5.3)].

Weaning and Discontinuation

Avoid abrupt discontinuation of GENOSYL [see Warnings and Precautions (5.1)]. To wean GENOSYL, down titrate in several steps, pausing several hours at each step to monitor for hypoxemia.

3 DOSAGE FORMS AND STRENGTHS

GENOSYL (nitric oxide) is a gas available at concentrations up to 800 ppm [see Description (11)].

4 CONTRAINDICATIONS

GENOSYL is contraindicated in neonates dependent on right-to-left shunting of blood.

5 WARNINGS AND PRECAUTIONS

5.1 Rebound Pulmonary Hypertension Syndrome following Abrupt Discontinuation

Wean from GENOSYL [see Dosage and Administration (2.2)]. Abrupt discontinuation of GENOSYL may lead to worsening oxygenation and increasing pulmonary artery pressure, i.e., Rebound Pulmonary Hypertension Syndrome. Signs and symptoms of Rebound Pulmonary Hypertension Syndrome include hypoxemia, systemic hypotension, bradycardia, and decreased cardiac output. If Rebound Pulmonary Hypertension occurs, reinstate GENOSYL therapy immediately.

5.2 Hypoxemia from Methemoglobinemia

Nitric oxide combines with hemoglobin to form methemoglobin, which does not transport oxygen. Methemoglobin levels increase with the dose of GENOSYL; it can take 8 hours or more before steady-state methemoglobin levels are attained. Monitor methemoglobin and adjust the dose of GENOSYL to optimize oxygenation.

If methemoglobin levels do not resolve with decrease in dose or discontinuation of GENOSYL, additional therapy may be warranted to treat methemoglobinemia [see Overdosage (10)] .

5.3 Airway Injury from Nitrogen Dioxide

Nitrogen dioxide (NO2) forms in gas mixtures containing NO and O2. Nitrogen dioxide may cause airway inflammation and damage to lung tissues.

If there is an unexpected change in NO2concentration, or if the NO2concentration reaches 0.5 ppm when measured in the breathing circuit, then the delivery system should be assessed in accordance with the GENOSYL Delivery System Operator's Manual troubleshooting section, and the NO2analyzer should be recalibrated. The dose of GENOSYL and/or FiO2should be adjusted as appropriate.

5.4 Worsening Heart Failure

Patients with left ventricular dysfunction treated with GENOSYL may experience pulmonary edema, increased pulmonary capillary wedge pressure, worsening of left ventricular dysfunction, systemic hypotension, bradycardia and cardiac arrest. Discontinue GENOSYL while providing symptomatic care.

6 ADVERSE REACTIONS

The following adverse reactions are discussed elsewhere in the label;

Hypoxemia [see Warnings and Precautions (5.2)]

Worsening Heart Failure [see Warnings and Precautions (5.4)]

6.1 Clinical Trials Experience

Because clinical trials are conducted under widely varying conditions, adverse reaction rates observed in the clinical trials of a drug cannot be directly compared to rates in the clinical trials of another drug and may not reflect the rates observed in practice. The adverse reaction information from the clinical studies does, however, provide a basis for identifying the adverse events that appear to be related to drug use and for approximating rates.

Controlled studies have included 325 patients on nitric oxide doses of 5 to 80 ppm and 251 patients on placebo. Total mortality in the pooled trials was 11% on placebo and 9% on nitric oxide gas for inhalation, a result adequate to exclude nitric oxide mortality being more than 40% worse than placebo.

In both the NINOS and CINRGI studies, the duration of hospitalization was similar in nitric oxide gas for inhalation and placebo-treated groups.

From all controlled studies, at least 6 months of follow-up is available for 278 patients who received nitric oxide gas and 212 patients who received placebo. Among these patients, there was no evidence of an adverse effect of treatment on the need for re-hospitalization, special medical services, pulmonary disease, and neurological sequelae.

In the NINOS study, treatment groups were similar with respect to the incidence and severity of intracranial hemorrhage, Grade IV hemorrhage, periventricular leukomalacia, cerebral infarction, seizures requiring anticonvulsant therapy, pulmonary hemorrhage, or gastrointestinal hemorrhage.

In CINRGI, the only adverse reaction (>2% higher incidence on nitric oxide gas for inhalation than on placebo) was hypotension (14% vs. 11%).

6.2 Postmarketing Experience

Post marketing reports of accidental exposure to nitric oxide for inhalation in hospital staff have been associated with chest discomfort, dizziness, dry throat, dyspnea, and headache.

7 DRUG INTERACTIONS

7.1 Nitric Oxide Donor Agents

Nitric oxide donor agents such as prilocaine, sodium nitroprusside and nitroglycerine may increase the risk of developing methemoglobinemia.

8 USE IN SPECIFIC POPULATIONS

8.4 Pediatric Use

The safety and efficacy of nitric oxide for inhalation has been demonstrated in term and near-term neonates with hypoxic respiratory failure associated with evidence of pulmonary hypertension [see Clinical Studies (14.1)] . Additional studies conducted in premature neonates for the prevention of bronchopulmonary dysplasia have not demonstrated substantial evidence of efficacy [see Clinical Studies (14.3)]. No information about its effectiveness in other age populations is available.

8.5 Geriatric Use

Nitric oxide is not indicated for use in the adult population.

10 OVERDOSAGE

Overdosage with nitric oxide gas is manifest by elevations in methemoglobin and pulmonary toxicities associated with inspired NO2. Elevated NO2may cause acute lung injury. Elevations in methemoglobin reduce the oxygen delivery capacity of the circulation. In clinical studies, NO2levels >3 ppm or methemoglobin levels >7% were treated by reducing the dose of, or discontinuing, nitric oxide gas.

Methemoglobinemia that does not resolve after reduction or discontinuation of therapy can be treated with intravenous vitamin C, intravenous methylene blue, or blood transfusion, based upon the clinical situation.

11 DESCRIPTION

GENOSYL (nitric oxide) is administered by inhalation. Nitric oxide is a pulmonary vasodilator. Nitric oxide is generated from liquid dinitrogen tetroxide (N2O4) by the Cassette in the GENOSYL Delivery System. Upon initiation of GENOSYL Delivery System, the liquid N2O4is heated and the equilibrium shifts to nitrogen dioxide (NO2) gas. The NO2is then converted into nitric oxide (NO) using the antioxidant Cartridges, and nitric oxide is delivered to the patient by means of a ventilator or a nasal cannula. The amount of nitric oxide administered to the patient is set by controlling the temperature of the N2O4liquid module, which controls the pressure inside the liquid module, which in turn controls the mass of NO2that is sent to the primary Cartridges, and hence the mass of nitric oxide. The mass flow of nitric oxide, together with the air from the pump, control the nitric oxide concentration. A nitric oxide sensor monitors the nitric oxide in the patient line. GENOSYL Delivery System is designed to deliver a controlled level of nitric oxide blended with breathing air or oxygen-enriched breathing air.

The GENOSYL Delivery System controls the flow of nitric oxide mixed with air delivered to the patient.

The structural formula of nitric oxide (NO) is shown below:

12 CLINICAL PHARMACOLOGY

12.1 Mechanism of Action

Nitric oxide relaxes vascular smooth muscle by binding to the heme moiety of cytosolic guanylate cyclase, activating guanylate cyclase and increasing intracellular levels of cyclic guanosine 3',5'-monophosphate, which then leads to vasodilation. When inhaled, nitric oxide selectively dilates the pulmonary vasculature, and because of efficient scavenging by hemoglobin, has minimal effect on the systemic vasculature.

GENOSYL appears to increase the partial pressure of arterial oxygen (PaO2) by dilating pulmonary vessels in better ventilated areas of the lung, redistributing pulmonary blood flow away from lung regions with low ventilation/perfusion (V/Q) ratios toward regions with normal ratios.

12.2 Pharmacodynamics

Effects on Pulmonary Vascular Tone in PPHN

Persistent pulmonary hypertension of the newborn (PPHN) occurs as a primary developmental defect or as a condition secondary to other diseases such as meconium aspiration syndrome (MAS), pneumonia, sepsis, hyaline membrane disease, congenital diaphragmatic hernia (CDH), and pulmonary hypoplasia. In these states, pulmonary vascular resistance (PVR) is high, which results in hypoxemia secondary to right-to-left shunting of blood through the patent ductus arteriosus and foramen ovale. In neonates with PPHN, nitric oxide gas for inhalation improves oxygenation (as indicated by significant increases in PaO2).

12.3 Pharmacokinetics

The pharmacokinetics of nitric oxide has been studied in adults.

Absorption and Distribution

Nitric oxide is absorbed systemically after inhalation. Most of it traverses the pulmonary capillary bed where it combines with hemoglobin that is 60% to 100% oxygen-saturated. At this level of oxygen saturation, nitric oxide combines predominantly with oxyhemoglobin to produce methemoglobin and nitrate. At low oxygen saturation, nitric oxide can combine with deoxyhemoglobin to transiently form nitrosylhemoglobin, which is converted to nitrogen oxides and methemoglobin upon exposure to oxygen. Within the pulmonary system, nitric oxide can combine with oxygen and water to produce nitrogen dioxide and nitrite, respectively, which interact with oxyhemoglobin to produce methemoglobin and nitrate. Thus, the end products of nitric oxide that enter the systemic circulation are predominantly methemoglobin and nitrate.

Metabolism

Methemoglobin disposition has been investigated as a function of time and nitric oxide exposure concentration in neonates with respiratory failure. The methemoglobin (MetHb) concentration-time profiles during the first 12 hours of exposure to 0, 5, 20, and 80 ppm nitric oxide are shown in Figure 1.

Methemoglobin concentrations increased during the first 8 hours of nitric oxide exposure. The mean methemoglobin level remained below 1% in the placebo group and in the 5 ppm and 20 ppm nitric oxide gas groups, but reached approximately 5% in the 80 ppm nitric oxide gas group. Methemoglobin levels >7% were attained only in patients receiving 80 ppm, where they comprised 35% of the group. The average time to reach peak methemoglobin was 10 ± 9 (SD) hours (median, 8 hours) in these 13 patients, but one patient did not exceed 7% until 40 hours.

Elimination

Nitrate has been identified as the predominant nitric oxide metabolite excreted in the urine, accounting for >70% of the nitric oxide dose inhaled. Nitrate is cleared from the plasma by the kidney at rates approaching the rate of glomerular filtration.

13 NONCLINICAL TOXICOLOGY

13.1 Carcinogenesis, Mutagenesis, Impairment of Fertility

No evidence of a carcinogenic effect was apparent, at inhalation exposures up to the recommended dose (20 ppm), in rats for 20 hr/day for up to two years. Higher exposures have not been investigated.

Nitric oxide gas has demonstrated genotoxicity in Salmonella (Ames Test), human lymphocytes, and after in vivo exposure in rats. There are no animal or human studies to evaluate nitric oxide for effects on fertility.

14 CLINICAL STUDIES

14.1 Treatment of Hypoxic Respiratory Failure (HRF)

The efficacy of nitric oxide gas was investigated in term and near-term newborns with hypoxic respiratory failure (HRF) resulting from a variety of etiologies. Inhalation of nitric oxide gas reduces the oxygenation index (OI= mean airway pressure in cm H2O × fraction of inspired oxygen concentration [FiO2]× 100 divided by systemic arterial concentration in mmHg [PaO2]) and increases PaO2 [see Clinical Pharmacology (12.1)].

NINOS Study

The Neonatal Inhaled Nitric Oxide Study (NINOS) was a double-blind, randomized, placebo-controlled, multicenter trial in 235 neonates with hypoxic respiratory failure. The objective of the study was to determine whether inhaled nitric oxide would reduce the occurrence of death and/or initiation of extracorporeal membrane oxygenation (ECMO) in a prospectively defined cohort of term or near-term neonates with hypoxic respiratory failure unresponsive to conventional therapy. Hypoxic respiratory failure was caused by meconium aspiration syndrome (MAS; 49%), pneumonia/sepsis (21%), idiopathic primary pulmonary hypertension of the newborn (PPHN; 17%), or respiratory distress syndrome (RDS; 11%). Infants ≤14 days of age (mean, 1.7 days) with a mean PaO2of 46 mmHg and a mean oxygenation index (OI) of 43 cm H2O / mmHg were initially randomized to receive 100% O2with (n=114) or without (n=121) 20 ppm nitric oxide for up to 14 days. Response to study drug was defined as a change from baseline in PaO230 minutes after starting treatment (full response = >20 mmHg, partial = 10–20 mmHg, no response = <10 mmHg). Neonates with a less than full response were evaluated for a response to 80 ppm nitric oxide or control gas. The primary results of this study are presented in Table 1.

Table 1: Summary of Clinical Results from Hypoxic Respiratory Failure Study
 | Control (n=121) | Nitric Oxide gas (n=114) | P value
Death or ECMO [Extracorporeal membrane oxygenation] , [Death or need for ECMO was the primary end point of this study] | 77 (64%) | 52 (46%) | 0.006
Death | 20 (17%) | 16 (14%) | 0.60
ECMO | 66 (55%) | 44 (39%) | 0.014

Although the incidence of death by 120 days of age was similar in both groups (NO, 14%; control 17%), significantly fewer infants in the nitric oxide group required ECMO compared with controls (39% vs. 55%, p = 0.014). The combined incidence of death and/or initiation of ECMO showed a significant advantage for the nitric oxide treated group (46% vs. 64%, p = 0.006). The nitric oxide group also had significantly greater increases in PaO2and greater decreases in the OI and the alveolar-arterial oxygen gradient than the control group (p<0.001 for all parameters). Significantly more patients had at least a partial response to the initial administration of study drug in the nitric oxide group (66%) than the control group (26%, p<0.001). Of the 125 infants who did not respond to 20 ppm nitric oxide control, similar percentages of NO-treated (18%) and control (20%) patients had at least a partial response to 80 ppm nitric oxide gas for inhalation or control drug, suggesting a lack of additional benefit for the higher dose of nitric oxide. No infant had study drug discontinued for toxicity. Inhaled nitric oxide gas had no detectable effect on mortality. The adverse events collected in the NINOS trial occurred at similar incidence rates in both treatment groups [see Adverse Reactions (6.1)] . Follow-up exams were performed at 18-24 months for the infants enrolled in this trial. In the infants with available follow-up, the two treatment groups were similar with respect to their mental, motor, audiologic, or neurologic evaluations.

CINRGI Study

This study was a double-blind, randomized, placebo-controlled, multi-center trial of 186 term and near-term neonates with pulmonary hypertension and hypoxic respiratory failure. The primary objective of the study was to determine whether nitric oxide gas would reduce the receipt of ECMO in these patients. Hypoxic respiratory failure was caused by MAS (35%), idiopathic PPHN (30%), pneumonia/sepsis (24%), or RDS (8%). Patients with a mean PaO2of 54 mmHg and a mean OI of 44 cm H2O / mmHg were randomly assigned to receive either 20 ppm nitric oxide gas (n=97) or nitrogen gas (placebo; n=89) in addition to their ventilatory support. Patients who exhibited a PaO2>60 mmHg and a pH < 7.55 were weaned to 5 ppm nitric oxide gas or placebo. The primary results from the CINRGI study are presented in Table 2.

Table 2: Summary of Clinical Results from Persistent Pulmonary Hypertension of the Newborn Study
 | Placebo | Nitric oxide gas | P value
ECMO [Extracorporeal membrane oxygenation] , [ECMO was the primary end point of this study] | 51/89 (57%) | 30/97 (31%) | <0.001
Death | 5/89 (6%) | 3/97 (3%) | 0.48

Significantly fewer neonates in the nitric oxide gas group required ECMO compared to the control group (31% vs. 57%, p<0.001). While the number of deaths were similar in both groups (Nitric oxide gas, 3%; placebo, 6%), the combined incidence of death and/or receipt of ECMO was decreased in the nitric oxide gas group (33% vs. 58%, p<0.001).

In addition, the nitric oxide gas group had significantly improved oxygenation as measured by PaO2, OI, and alveolar-arterial gradient (p<0.001 for all parameters). Of the 97 patients treated with nitric oxide gas, 2 (2%) were withdrawn from study drug due to methemoglobin levels >4%. The frequency and number of adverse events reported were similar in the two study groups [see Adverse Reactions (6.1)].

In clinical trials, reduction in the need for ECMO has not been demonstrated with the use of inhaled nitric oxide in neonates with congenital diaphragmatic hernia (CDH).

14.2 Ineffective in Adult Respiratory Distress Syndrome (ARDS)

In a randomized, double-blind, parallel, multicenter study, 385 patients with adult respiratory distress syndrome (ARDS) associated with pneumonia (46%), surgery (33%), multiple trauma (26%), aspiration (23%), pulmonary contusion (18%), and other causes, with PaO2/FiO2<250 mmHg despite optimal oxygenation and ventilation, received placebo (n=193) or nitric oxide gas (n=192), 5 ppm, for 4 hours to 28 days or until weaned because of improvements in oxygenation. Despite acute improvements in oxygenation, there was no effect of nitric oxide gas on the primary endpoint of days alive and off ventilator support. These results were consistent with outcome data from a smaller dose ranging study of nitric oxide (1.25 to 80 ppm). GENOSYL (nitric oxide) for inhalation is not indicated for use in ARDS.

14.3 Ineffective in Prevention of Bronchopulmonary Dysplasia (BPD)

The safety and efficacy of nitric oxide gas for the prevention of chronic lung disease [bronchopulmonary dysplasia (BPD)] in neonates ≤ 34 weeks gestational age requiring respiratory support has been studied in four large previously conducted multicenter, double-blind, placebo-controlled clinical trials in a total of 2,600 preterm infants. Of these, 1,290 received placebo, and 1,310 received inhaled nitric oxide at doses ranging from 5-20 ppm, for treatment periods of 7-24 days duration. The primary endpoint for these studies was alive and without BPD at 36 weeks postmenstrual age (PMA). The need for supplemental oxygen at 36 weeks PMA served as a surrogate endpoint for the presence of BPD. Overall, efficacy for the prevention of bronchopulmonary dysplasia in preterm infants was not established. There were no meaningful differences between treatment groups with regard to overall deaths, methemoglobin levels, or adverse events commonly observed in premature infants, including intraventricular hemorrhage, patent ductus arteriosus, pulmonary hemorrhage, and retinopathy of prematurity.

The use of GENOSYL (nitric oxide) for prevention of BPD in preterm neonates ≤34 weeks gestational age is not recommended.

16 HOW SUPPLIED/STORAGE AND HANDLING

GENOSYL Delivery System Cassettes produce at least 216 liters of 800 ppm nitric oxide gas (at standard temperature and pressure, STP) (NDC 72385-002-01).

GENOSYL Delivery System External Transport Cassettes produce at least 73 liters of 800 ppm nitric oxide gas (at standard temperature and pressure, STP) (NDC 72385-003-01).

STORAGE AND HANDLING

Store at 20°C to 25°C (68°F to 77°F) with excursions permitted between 15°C and 30°C (59°F and 86°F) [see USP Controlled Room Temperature].

The GENOSYL Delivery System must be used with antioxidant Cartridges not older than 12 months from the manufacturing date.

Occupational Exposure

The exposure limit set by the Occupational Safety and Health Administration (OSHA) for nitric oxide is 25 ppm, and for NO2the limit is 5 ppm.

Rx Only

VERO Biotech and GENOSYL are registered trademarks of VERO Biotech.

© 2024 VERO Biotech

Manufactured by:

VERO BIOTECH

387 Nerem Street NW

Suite 125

Atlanta, GA 30313, USA
[602604]

INSTRUCTIONS FOR USE

VĒRO
BIOTECH

GENOSYL®
DELIVERY SYSTEM

FOR DELIVERY OF
GENOSYL®
(NITRIC OXIDE)
GAS FOR INHALATION

OPERATOR'S MANUAL

Technical Support: 877.337.4118

Company Confidential
Part No. 602502 Rev. I

DO NOT COPY

VERO Biotech Inc.
387 Nerem Street NW, Suite 125
Atlanta, GA 30313 USA

WARNINGS, CAUTIONS, AND NOTES

Please read all Warnings and Cautions in this Operator's Manual prior to using the GENOSYL DS.

MR Conditional Safety Information

The GENOSYL DS may be safely used in the MR environment under the following conditions. Failure to follow these conditions may result in injury.

- Maximum static magnetic field of 100 Gauss (0.01mT)
- Device remains outside the scanner bore
- Preparation protocols described in the Warnings section titled "Use in the MR Environment" must be followed before MR procedure

Image Artifacts:

When the GENOSYL DS is battery powered, no image artifacts are expected. When powered using a wall outlet, minor noise is expected.

Throughout this Operator's Manual, warnings, cautions, and notes will be displayed in the following manner.

WARNING

The warning box will alert the user to possible injury, death, or serious adverse reactions associated with the use or misuse of the device.

CAUTION

The caution box will alert the user about proper use of the equipment and any conditions that could result in equipment damage or failure. The user should read and adhere to all warnings and cautions.

NOTE

The note box provides information, clarification, or supplemental information to assist and educate the user on the use of the equipment.

A complete list of Warnings and Cautions for the GENOSYL DS are shown below. Where appropriate, some of these will also be shown throughout this manual.

WARNINGS

Please consult the package insert for a complete list of contraindications.

Alarms

- ALWAYS acknowledge and follow information provided from alarms. An alarm indicates an abnormal condition, and ignoring alarms can result in possible injury, death, or serious adverse reactions.
- ALWAYS use clinical judgement when setting upper or lower alarm limits. Failure to do so could result in possible injury or death.

Consoles

- ALWAYS have a second Console present and properly connected when a Dosing Console is connected to the patient. If the Dosing Console malfunctions, switch to the Back-up Console. If the Back-up Console is not available or properly connected, this may result in patient injury or death.
- DO NOT clean the GENOSYL DS with the power connected and the System turned ON, as this may lead to injury (e.g., shock). Unplug AC/DC power supply external to the System prior to cleaning.
- NEVER modify the equipment. Modifications of the equipment may result in malfunction, which may result in a fire, shock, injury, or death.
- NEVER turn the rear power switch OFF until the System has gone through a controlled shutdown or instructed by VERO Technical Support. Turning the rear power switch OFF prematurely (e.g., while it is still in use) will immediately shut down the device. This may result in interruption in NO delivery to the patient, which may cause injury or death.

Cassette

- DO NOT use the Cassette if the Cassette State Window is not blue. A Cassette State Window that is any color other than blue may affect the Cassette's ability to provide the correct NO dosage to the patient, which may cause injury or death.
- DO NOT use a Cassette that is beyond its expiration date. Using an expired Cassette may affect the Cassette's ability to provide the correct NO dosage to the patient, which may cause injury or death.
- MAKE SURE the System stabilizes to the prescribed concentration (ppm) of NO prior to leaving the Console unattended. Failure to do so could result in under delivery of the target NO, leading to injury or harm.
- ALWAYS replace a Cassette once depleted. A depleted Cassette will interrupt patient dosing and can lead to underdosing and/or injury to the patient.
- ALWAYS follow Cassette inspection instructions prior to Cassette insertion. Not inspecting the Cassette prior to insertion may lead to using a faulty Cassette, resulting in injury.

Use in the MR Environment

- The GENOSYL DS is classified as MR Conditional with MR scanners of 1.5 or 3.0 Tesla strength ONLY in areas where the field strength is less than 100 gauss.
- ALWAYS operate at a fringe field of less than 100 gauss. This device contains ferromagnetic components and may experience strong attraction close to the magnet.
- DO NOT exceed 100 gauss; System operation may be impacted. Confirm Cart caster lock function. Optionally connect tether.
- NEVER use the GENOSYL DS in the MR scanner room without gauss alarms installed.
- ALWAYS verify at least one gauss alarm is functioning properly prior to use in the MR environment.
- DO NOT use the GENOSYL DS in the MR environment if neither gauss alarm is functional.
- ALWAYS move System away from the MR scanner if the gauss alarm sounds. The gauss alarm will sound if the System is too close to the MR scanner. Move System away from the MR scanner until the gauss alarm stops sounding.
- ALWAYS verify that the GENOSYL DS Cart casters are locked after positioning the System in the MR scanner room.
- ALWAYS verify that the GENOSYL DS is securely attached to the Cart.
- ALWAYS arrange power cord, MR patient gas sample line, and NO delivery line to avoid entanglement, strangulation and/or a trip hazard.
- DO NOT use the GENOSYL DS in the MR environment if the Cart moves when the brake caster locks are engaged.
- NEVER perform NO or NO2calibration within the MR scanner room. Calibration equipment is a potential projectile hazard.

Transport

- ALWAYS ensure the GENOSYL DS Dosing and Back-up Consoles are securely affixed to the External Transport Mounts when the System will be used in a transport vehicle.
- ALWAYS ensure Consoles are placed into External Transport Mode before inserting a Cassette for external transport outside of the hospital.
- ONLY use External Transport Cassettes, identified by orange color and transport sticker, in external transport outside of the hospital.
- ALWAYS ensure the External Transport Mounts are secured during patient transport, per hospital protocols.

Use with Anesthesia Gas Machines

- ALWAYS use the Anesthesia Gas Machine (AGM) in accordance with the manufacturer's instructions.
- The flow out of the anesthesia gas machine via the INSPIRATORY breathing circuit limb must pass through the GENOSYL DS Gas Injection Assembly.
- The GENOSYL DS injects and samples gas from the patient respiratory circuit which may affect the triggering sensitivity of the anesthesia gas machine (AGM). ALWAYS ensure the trigger sensitivity of the AGM is checked after connecting the GENOSYL DS to the breathing circuit and starting iNO delivery or when the dose is changed and adjust trigger sensitivity as necessary. Failure to do so may lead to AGM auto cycling or apnea alarm.
- ALWAYS ensure the patient disconnect and high–pressure alarms are used with the AGM.
- Ensure the Injection Assembly and the Gas Sample Tee are BOTH inserted on the inspiratory limb of the circuit.

Connections

- ALWAYS follow pre-use setup instructions for the routing and connections of tubing to avoid patient strangulation.
- MAKE SURE the System has all tubing connected as described in the instructions. Not connecting all tubing may result in inaccurate dosage and harm the patient.
- NEVER touch the electrical connectors of the System or its accessories, and the patient simultaneously. If the user touches another device with a ground-fault failure and simultaneously touches the GENOSYL DS, this can result in injury (e.g., shock) should a grounding failure be present.

Battery

- ONLY properly trained personnel should replace the battery. Incorrectly replacing the battery may result in a hazard such as excessive temperatures, fire, or explosion.
- MAKE SURE the GENOSYL DS is connected to AC wall power to charge the battery a minimum of once every 3 months to maintain a minimum battery charge. Failure to recharge the Console battery for extended timeframes may result in full discharge of the battery. If a Battery Error message occurs during startup of the System, contact Technical Support at 877-337-4118 for assistance.

User

- ONLY intended users who are experienced in the use of this System should use this device. US federal law restricts device use to licensed medical professionals. If device is used by unintended users, device can be misused and lead to injury or death.

Alternative Means of Ventilation

- ALWAYS ensure that the manual flow displayed on the Console matches the flow set into the resuscitation bag. Incorrect flow settings may result in an incorrect estimation of NO delivery. If the flow into the manual equipment is too low, there is risk of overdosing the patient with NO.
- ALWAYS squeeze the bag several times, after starting fresh gas flow, to empty residual gas in the bag prior to using the System to ventilate a patient. Failure to do so could result in higher NO2levels being delivered to the patient.
- ALWAYS use the smallest bag adequate to deliver the desired tidal volume. Failure to do so could result in higher NO2levels being delivered to the patient.

Patient Monitoring

- ALWAYS constantly monitor the patient. System malfunctions can occur if device and patient are not monitored and can result in injury or death. Careful monitoring is required by care personnel whenever the System is used on a patient. The use of an alarm and a monitoring system does not give an absolute assurance of warning for every malfunction that may occur. Certain alarms may require immediate response.

Use with Breathing Devices

- ONLY use a manual resuscitation bag with the GENOSYL DS for a short time (e.g., less than one hour) when on battery only. Otherwise, the System may shut off and may result in injury or death.
- The GENOSYL DS injects and samples gas from the patient respiratory circuit which may affect the triggering sensitivity of the ventilator. ALWAYS ensure the trigger sensitivity of the ventilator is checked after connecting the GENOSYL DS to the breathing circuit or when the dose is changed and adjust trigger sensitivity as necessary. Failure to do so may lead to ventilator auto cycling or apnea alarm.
- ALWAYS ensure the patient disconnect and high-pressure alarms are used with the ventilator.
- ONLY use the GENOSYL DS with Bio-Med Crossvent 2+ with Constant Flow ON. Not doing so may lead to elevated NO2 levels or dose variability.

Set-up

- ONLY VERO Biotech authorized equipment technicians are to perform the initial System set-up prior to initial use. Failure to use an authorized equipment technician can result in a patient or user injury.
- ONLY store the GENOSYL DS as outlined in the storage instructions. Not storing the device in alignment with its storage instructions can cause the device to be unsafe and lead to injury or death.
- AVOID using the GENOSYL DS adjacent to or stacked with other equipment, as it may result in improper operation. If such use is necessary, this equipment and the other equipment should be observed to verify that they are operating normally.
- DO NOT use accessories or cables other than those specified or provided by the manufacturer of this equipment, as this may result in increased electromagnetic emissions or decreased electromagnetic immunity of this equipment and result in improper operation.
- DO NOT place portable RF communications equipment (including peripherals such as antenna cables and external antennas) closer than 30cm (12 inches) to any part of the GENOSYL DS, including cables specified. Otherwise, degradation of the performance of this equipment could occur, resulting in injury.
- Only connect to a power outlet with protective earth. Failure to connect to an outlet with protective earth may result in an electrical shock.

Troubleshooting

- ALWAYS ensure patient safety before troubleshooting (such as an activated alarm) or replacing a problematic item. Not monitoring the patient prior to attending to an alarm can result in injury or death.

Calibration

- ONLY use the calibration gas pressure regulators supplied by the manufacturer. Pressure regulators not supplied by the manufacturer may damage the sensors and may lead to patient injury.
- ALWAYS verify the correct NIST traceable calibration gas is being used and confirm the expiration date of the calibration gas prior to performing calibration. The use of incorrect or expired gas may result in inaccurate sensor readings and can lead to patient injury.

Cleaning and Maintenance

- NEVER submerge the GENOSYL DS, Cassettes, or non-disposable Adaptive Sensor Cable. Submerging in liquids will damage the System and could cause electrical shorts which may result in injury or death.

Water Trap

- ALWAYS empty Water Trap when prompted by the System, and when the trap is more than half full. Allowing the Water Trap to completely fill will occlude the Sample Line which will interrupt patient gas NO, NO2, and O2concentration monitoring. Failure to monitor the patient gas NO, NO2, and O2concentrations may result in patient injury.
- ALWAYS conduct Water Trap / Sample Line Leak Test every time you empty and replace the Water Trap, as failure to do so may lead to an incorrect NO reading, which can result in injury or death.
- ALWAYS use a Water Trap supplied by the manufacturer. Using an incorrect Water Trap could result in non-functioning or inaccurate sensor readings.

Use Outside of Product Labeling

- ALWAYS use the GENOSYL DS in accordance with the indications, usage, contraindications, warnings, and precautions described in the GENOSYL prescribing information and labeling. Refer to latest approved prescribing information and labeling prior to use.
- The approved patient population for the GENOSYL DS as specified in the drug labeling for GENOSYL (nitric oxide) for inhalation, is limited to neonates. The GENOSYL DS is not intended to be used in other patient populations.
- ONLY use the GENOSYL DS, its parts, and accessories as instructed. Using non-specified components may result in product malfunction, injury, or death
- ONLY trained personnel should operate the GENOSYL DS. Failure to do so can result in injury or death.
- ONLY mechanical ventilators validated with the GENOSYL DS should be used. Not using a validated ventilator system can result in injury or harm.

CAUTIONS

Supplied Instructions

- ALWAYS refer to the instructions supplied with all equipment to be used in conjunction with the GENOSYL DS for their intended uses, contraindications, and potential complications. Misuse of the device or its components may damage the device.

Cassette

- DO NOT remove Cassette from packaging until ready to use. External packaging is designed to protect the Cassette from damage and/or contamination.
- User should always have a secondary Cassette inserted in the Dosing Console and preheated in order for auto transition to occur. User should replace depleted Cassette as soon as possible after ejection.

Consoles

- ALWAYS operate the Console on a level surface to avoid potential interruption to nitric oxide (NO) delivery.
- ONLY use recommended cleaning agents or a damp cloth to clean the Console and limit use of liquids around Console. Excess water can permanently damage the device.
- ONLY use the GENOSYL DS with the power cord supplied by the manufacturer. Use of a generic power cord may cause output voltage instability leading to a touch screen failure.
- ALWAYS ensure the power cord is firmly seated into the power supply and the wall outlet. A loose connection can result in damage to the device or faulty operation.
- Prolonged use in dry environments without humidification will damage the gas sensors. Supplemental humidification providing greater than 20% relative humidity (RH) in the patient circuit is recommended.

Use with Breathing Devices

- When using spontaneous breathing modeson respiratory device, NO2levels may exceed 3.0 ppm NO when dosing ≥ 57 ppm NO into 100% FiO2and maximum bias flow, resulting in nitric oxide delivery interruption. Once sample value of NO2is below 3.0 ppm, the Console will auto resume delivery of NO at set dose. Refer to Section 12.1.5 Table 13for additional information.
- When using non-spontaneous breathing modeson respiratory device NO2levels may exceed 3.0 ppm when dosing ≥ 63 ppm NO into 100% FiO2and maximum bias flow, resulting in nitric oxide delivery interruption. Once sample value of NO2is below 3.0 ppm, the Console will auto resume delivery of NO at set dose. Refer to Section 12.1.5 Table 13for additional information.

Use with Anesthesia Gas Machines

- The Adaptive Sensor is recommended for use with anesthesia gas machines (AGMs). When using an AGM without the Adaptive Sensor, transient dose excursions outside of the set NO dose may occur during Cassette transition, and changes in breathing circuit flow may cause fluctuations in measured levels of NO and NO2when using the manual ventilation bag integrated with the AGM.
- When using anesthesia gas machines, NO2levels may exceed 3.0 ppm when dosing ≥ 58 ppm NO into 100% FiO2, resulting in nitric oxide delivery interruption. Once sample value of NO2is below 3.0 ppm, the Console will auto resume delivery of NO at set dose.
- DO NOT use in environments with <20% relative humidity (RH) in the absence of supplemental humidification. Prolonged use in dry environments without humidification will damage the gas sensors. GENOSYL DS was validated with listed AGMs using a Heat Moisture Exchanger (HME) and was not tested with heated humidification connected to the respiratory circuit.
- Rebreathing validation testing was performed with semi-closed breathing systems. Non-rebreathing validation testing was perfumed with semi-open breathing systems. The GENOSYL DS has not been evaluated with fully open or fully closed anesthesia breathing systems.

Gas Sampling During Aerosol Delivery

- Pneumatic Nebulizers will dilute the delivered nitric oxide dose.

Calibration

- ALWAYS perform a full-scale calibration of the GENOSYL DS when prompted by the System prior to use.
- ALWAYS confirm the correct flow direction of the installed one-way check valve in the sampling tee to avoid over pressurization of the sample system and damage to the device.

Cleaning and Maintenance

- ALWAYS follow maintenance instructions in this manual for your safety and to prevent damage to the System.
- ALWAYS power down the GENOSYL DS Console when not in use.
- DO NOT sterilize (e.g., autoclave, gas sterilize) any of the components of the System, as this may compromise performance.
- DO NOT use harsh cleaning agents. Doing so may impair the structural integrity and/or function of the device.
- DO NOT touch or rub the display screen with abrasive cleaning compounds, as they may scratch and damage the screens.
- ALWAYS ensure the System is completely dry after cleaning before powering it ON. Failure to do so could result in equipment damage.

Switching OFF the System

- NEVER turn the rear power switch OFF until the System has gone through a controlled shutdown or instructed by VERO Technical Support. Turning the rear power switch OFF prematurely (e.g., while it is still in use) will immediately shut down the device and may cause improper operation upon restart.

Cart

- DO NOT stand or sit on the Cart. Standing or sitting on the Cart can damage the device.
- ALWAYS push or pull the Cart using the handle only. NOT doing so may result in damage to the device.

TABLE OF CONTENTS
WARNINGS, CAUTIONS, AND NOTES |  | 3
TABLE OF CONTENTS |  | 12
LIST OF TABLES |  | 16
LIST OF FIGURES |  | 17
ABBREVIATIONS, TERMINOLOGY, AND DEFINITIONS |  | 19
SYMBOLS |  | 21
GENOSYL DS PARTS / COMPONENTS |  | 23
1. | GENERAL INFORMATION | 32
1.1 | User Responsibility | 32
1.2 | General Information and Indications for Use | 33
1.3 | Principles of Operation | 34
1.4 | Exposure of Healthcare Providers to NO and NO2 | 38
2. | SYSTEM OVERVIEW | 42
2.1 | Frequently Used Functions | 42
2.2 | GENOSYL DS Cart and Consoles | 43
2.3 | Cassette | 49
2.4 | GENOSYL DS Ventilator Circuit Components | 51
2.5 | Gas Lines (detailed explanation) | 54
2.6 | Console Dosing Modes of Operation | 56
2.7 | Display Screen | 56
2.8 | Display "Menu" Tab Navigation | 57
2.9 | Display Screen Operational Buttons | 61
2.10 | Display Screen – Cassette Status Indicators | 63
2.11 | Display Screen - Adaptive Sensor Status | 67
2.12 | Cassette Insertion into Console | 68
2.13 | Water Trap / Sample Line Leak Test | 68
2.14 | Console Shutdown - Cassette Status Indicator | 69
2.15 | Battery Charge Status Indicator | 70
3. | SYSTEM SET-UP AND CONNECTIONS | 74
3.1 | GENOSYL DS Set-Up and Mechanical Ventilator Circuit Schematic | 74
3.2 | Connections to Various Breathing Systems | 74
3.2.1 | Conventional Ventilators | 75
3.2.2 | Non-Invasive Gas Delivery Systems | 79
3.3 | GENOSYL DS Ventilator Circuit Assembly Pre-Check | 81
3.4 | Assembling GENOSYL DS Injection Assembly with Adaptive Sensor and GENOSYL DS Mixer Assembly with Adaptive Sensor | 83
3.4.1 | GENOSYL DS Injection Assembly with Adaptive Sensor | 83
3.4.2 | GENOSYL DS Mixer Assembly with Adaptive Sensor | 84
3.5 | GENOSYL DS Console Connections | 86
3.5.1 | GENOSYL DS Gas Line Connections | 86
3.5.2 | GENOSYL DS Sample Line Extension Connection | 87
3.5.3 | Sample Line Filter Connection | 89
3.5.4 | GENOSYL DS Adaptive Sensor Cable Connection | 91
3.5.5 | GENOSYL DS Respiratory Circuit Connections | 91
3.6 | Manual Ventilation (Bag) Connection | 93
3.7 | Mechanical Ventilator Circuit Connections | 94
3.8 | Gas Sampling During Aerosol Delivery | 95
4. | SYSTEM START UP | 100
4.1 | Console Start-Up | 100
4.2 | Cassette Insertion & Water Trap / Sample Line Leak Test | 101
4.2.1 | Water Trap / Sample Line Leak Test Troubleshooting | 107
5. | NITRIC OXIDE ADMINISTRATION | 110
5.1 | Nitric Oxide Dose Set-Up and Administration | 110
5.1.1 | Setting a Dose when using a Circuit withan Adaptive Sensor | 110
5.1.2 | Setting a Dose when using a Circuit withoutan Adaptive Sensor | 112
5.2 | Adjusting the Dose | 113
5.3 | Replacement of a Depleted Cassette | 115
5.4 | Manual Mode | 116
5.4.1 | Manual Ventilation Use (Bagging) | 116
5.4.2 | Preset Manual Dosing Mode Flow Rate (OPTIONAL) | 119
5.4.3 | Resuming Primary Dosing | 119
5.5 | Console Use as a Back-up | 120
6. | CONSOLE SHUTDOWN AND CASSETTE DISPOSAL | 124
6.1 | Console Shutdown | 124
6.2 | Cassette Disposal | 128
7. | USING THE SYSTEM IN THE MR SCANNER ROOM | 132
7.1 | Connection to the Ventilator Breathing Circuit | 132
7.2 | Transferring to and from the MR Scanner Room | 133
8. | EXTERNAL TRANSPORT | 138
8.1 | External Transport Set-Up and Ventilator Circuit Schematics | 144
8.1.1 | Securing a Console in a Transport Mount | 144
8.1.2 | Connection to an International Bio-Med External Transport Ventilator Circuit | 145
8.1.3 | Connection to a Conventional External Transport Ventilator | 147
8.1.3.1 | Connection to a Conventional External Transport Ventilator using an Injection Assembly with Adaptive Sensor | 148
8.1.3.2 | Transport Ventilator Circuit Set-Up and Connections using Mixer Assembly with Adaptive Sensor | 151
8.2 | Using the GENOSYL DS for External Transport | 153
8.2.1 | Switching External Transport Mode ON | 153
8.2.2 | Inserting an External Transport Cassette | 155
8.2.3 | Setting a Dose in External Transport Mode with an Adaptive Sensor | 159
8.2.4 | Setting a Dose in External Transport Mode without an Adaptive Sensor | 161
8.2.5 | Adjusting a Dose in External Transport Mode | 163
8.2.6 | Using Manual Dosing Mode while External Transport Mode is Enabled | 164
8.2.7 | Resuming Primary Dosing while in External Transport Mode | 166
8.2.8 | Console Shutdown while in External Transport Mode | 167
8.2.9 | Switching External Transport Mode OFF | 171
9. | USE WITH ANESTHESIA GAS MACHINES | 174
8.1 | Connection to a Dual Limb Anesthesia Circuit | 176
8.2 | Connection Instructions for the GENOSYL DS to an Anesthesia Gas Machine | 177
10. | ALARMS, ALERTS, AND TROUBLESHOOTING | 184
10.1 | Alarms, Alerts, and Troubleshooting | 184
10.2 | On-screen Troubleshooting Module | 186
10.3 | High Priority Alarms and Messages | 189
10.4 | Medium Priority Alarms and Messages | 200
10.5 | Low Priority Alarms and Messages | 204
10.6 | Informational Messages | 205
10.7 | GaussAlert™ Alarm | 207
10.8 | Troubleshooting | 208
10.9 | Leak Detection Tool | 211
11. | SYSTEM MAINTENANCE | 216
11.1 | Calibration | 216
11.1.1 | Air Calibration | 217
11.1.2 | NO Calibration | 218
11.1.3 | NO2Calibration | 220
11.2 | Maintenance Schedule | 222
11.3 | Testing the GaussAlert™ Function | 222
11.4 | Water Trap Maintenance | 224
11.4.1 | Emptying the Water Trap | 224
11.4.2 | Water Trap Replacement | 225
11.5 | Battery | 225
11.6 | Cleaning | 226
11.6.1 | Enclosure, Connections, and Surfaces Other Than the Display | 226
11.6.2 | Display Screen | 227
11.6.3 | Cleaning the Gauss Alarms Mount | 227
11.7.1 | Cart / Console Storage | 228
11.7.2 | Cassette / Accessory Storage | 228
12. | MECHANICAL VENTILATION | 232
12.1 | Mechanical Ventilation | 232
12.1.1 | Oxygen Dilution | 232
12.1.2 | Minute Volume | 234
12.1.3 | Trigger Sensitivity | 234
12.1.4 | Maximum NO Delivery | 234
12.1.5 | Bias Flow and NO2 | 234
12.2 | Ventilator Compatibility | 236
13 | PRODUCT SPECIFICATIONS | 246
13.1 | System Performance | 246
13.2 | System Classification | 246
13.3 | Testing | 246
13.4 | Electrical | 247
13.5 | Power Supply | 247
13.6 | Battery | 247
13.6.1 | Battery Charge Status Indicator | 248
13.17 | Display | 248
13.8 | Mechanical | 248
13.9 | Environmental | 249
13.10 | GaussAlert™ Specifications | 249
13.11 | MR Signal-to-Noise Ratio and Artifact Dimension Analysis | 249
13.12 | EMI/EMC | 250
KEY WORD INDEX |  | 258

LIST OF TABLES
Table 1: Conventional Ventilator Compatibility Test Ranges | 76
Table 2: Non-Invasive Gas Delivery System Compatibility Test Ranges | 79
Table 3: External Transport Ventilation Devices Compatibility Testing Ranges | 140
Table 4: External Transport Equipment Specifications | 143
Table 5: Anesthesia Gas Machine Validation Compatibility Test Ranges | 175
Table 6: Anesthesia Gas Machine Tidal Volume Use Cases | 176
Table 7: Alarm Icon Descriptions | 184
Table 8: Alarm Characteristics | 185
Table 9: Alarm Ranges, Defaults and Dose Interruption Condition | 185
Table 10: Alarm conditions included in On-screen Troubleshooting Module | 187
Table 11: Recommended Cleaning Agents | 227
Table 12: Oxygen Dilution | 233
Table 13: NO Dose at which NO2exceeded 3ppm NO2Threshold when dosing at 100% FiO2and Maximum bias flow | 235
Table 14: Details of Validated Systems | 237
Table 15: Validated Compatibility with and without Inline Mixer | 241

LIST OF FIGURES
Figure 1: GENOSYL DS Console Front Panel | 34
Figure 2: Cassette Output Range | 35
Figure 3: Calculated Time to Hospital Cassette Depletion | 36
Figure 4: Calculated Time to External Transport Cassette Depletion | 36
Figure 5: GENOSYL DS Assembled Cart | 44
Figure 6: MR Conditional GENOSYL DS Front View | 45
Figure 7: MR Conditional GENOSYL DS Side View | 46
Figure 8: Front View GENOSYL DS Console | 47
Figure 9: Back View GENOSYL DS Console | 48
Figure 10: Right Side View GENOSYL DS Console | 48
Figure 11: Left Side View GENOSYL DS Console | 48
Figure 12: GENOSYL Cassette | 49
Figure 13: GENOSYL External Transport Cassette | 50
Figure 14: GENOSYL DS Gas Lines | 55
Figure 15: GENOSYL DS Display Screen | 56
Figure 16: Water Trap/Sample Line Leak Test | 69
Figure 17: Conventional Ventilator Circuit Set-Up and Connections using Injection Assembly with Adaptive Sensor to the GENOSYL DS and a Manual Bagging System | 77
Figure 18: Conventional Ventilator Circuit Set-Up and Connection using the Mixer Assembly with Adaptive Sensor to the GENOSYL DS and a Manual Bagging System | 78
Figure 19: Fisher and Paykel Optiflow Jr 2 Breathing Circuit | 79
Figure 20: Fisher and Paykel Optiflow Breathing Circuit | 80
Figure 21: GENOSYL DS Injection Assembly with Adaptive Sensor | 83
Figure 22: GENOSYL DS Mixer Assembly with Adaptive Sensor | 84
Figure 23: MR Scanner Room | 134
Figure 24: Display Navigation in External Transport Mode | 139
Figure 25: GENOSYL DS on External Transport Mount | 141
Figure 26: External Transport Cassette | 142
Figure 27: International Bio-Med Transport Ventilator Circuit Set-Up and Connections using Injection Assembly with Adaptive Sensor to the GENOSYL DS and a Manual Bagging System | 145
Figure 28: Transport Ventilator Circuit Set-Up and Connections using Injection Assembly with Adaptive Sensor to the GENOSYL DS and a Manual Bagging System | 148
Figure 29: Transport Ventilator Circuit Set-Up and Connections using Mixer Assembly with Adaptive Sensor to the GENOSYL DS and a Manual Bagging System | 151
Figure 30: Anesthesia Gas Machine Circuit Set-up and Connection to the GENOSYL DS without Inline Mixer | 177
Figure 31: Anesthesia Gas Machine Circuit Set-up and Connection to the GENOSYL DS with Inline Mixer | 177
Figure 32: On-screen Troubleshooting Menu | 187
Figure 33: Description of VERO On-screen Troubleshooting Module Navigation | 188
Figure 34: Screen displayed if recommended actions cannot address alarm condition, or alarm condition is active and on-screen troubleshooting support is not available | 189
Figure 35: "Alarms" tab display when a leak is suspected | 212
Figure 36: GaussAlert™ Test | 223
Figure 37: Cassette Output Range | 236

ABBREVIATIONS, TERMINOLOGY, AND DEFINITIONS
ABBREVIATION / TERMINOLOGY | DEFINITION
Adaptive Sensor Port | Port on the front of the Console that the Adaptive Sensor Cable plugs into.
AGM | Anesthesia Gas Machine
Back-up | A situation whereby the Back-up Console and its Cassette is activated in the event of a failure of the Dosing Console.
Back-up Console | The secondary Console used as a "Back-up" system to administer nitric oxide when the Dosing Console cannot be used.
BPM | Breaths per minute
Cassette | The Cassette contains the material used to make nitric oxide and when inserted into the Console is available for dosing the patient.
cmH20 | Centimeters of water / unit of pressure
Display | Electronic information panel located on the front of the Console.
Dosing Console | The Console that is actively dosing NO.
DS | Delivery System
Gas Sample Port | Port on the front of the Console at the Water Trap that measures NO, NO2and O2levels within the NO gas path prior to reaching the patient.
GENOSYL | Nitric oxide for inhalation
Hz | Hertz
Keypad | A Graphical User Interface function built into the Console display and used to enter the nitric oxide dose to be administered to the patient.
L/min | Liters per minute
LPM | Liters per minute
Mixer | Ventilator circuit accessory used to mix the ventilator gas with the gas supplied by the GENOSYL DS for specific ventilator and tidal volume use cases, per Section 12.2.
MRI | Magnetic Resonance Imaging
MR Scanner Bore | The MR scanner opening
MR Exclusion Zone | Area in the MR scanner room where the magnetic field is greater than 100 gauss
MR Scanner | The MR device for diagnostic imaging
MR Scanner Room | The room where the MR scanner is located
mT | Millitesla; Unit used to measure magnetic field
NICU | Neonatal Intensive Care Unit
NO | Nitric oxide
NO Injection Port | Port on the front of the Console that introduces the concentrated NO into the respiratory circuit.
NO2 | Nitrogen dioxide
N2O4 | Dinitrogen tetroxide
O2 | Oxygen
OD | Oxygen diameter
PEEP | Positive end-expiratory pressure
ppm | Parts er Million
psi | Pounds per square inch/ unit of pressure
System | The System (GENOSYL DS) consists of a Cart with two Consoles, Cassettes, and component parts used to set up the gas lines
v | Electrical Volts

SYMBOLS
Symbol | Symbol Name | Description
 | AC | Indicates power input specification is alternating current (AC).
 | Adaptive Sensor Port | Input port for Adaptive Sensor Cable
 | Atmospheric pressure limitation | To indicate the acceptable upper and lower limits of atmospheric pressure for transport and storage.
 | Attention | Indicates the need for the user to consult the instructions for use for important cautionary information such as warnings and precautions that cannot, for a variety of reasons, be presented on the medical device itself.
 | Batch Code | Indicates the batch code so that the batch or lot can be identified.
 | Calibration Port | Input port for calibration gas
 | Catalog or model number | Indicates the catalog number so that the medical device can be identified.
 | Consult instructions for use | Informs the user to consult the instructions for use.
 | Date of Manufacture | Indicates the date when the medical device was manufactured.
 | Do not reuse | Indicates a medical device that is intended for one use, or for use on a single patient during a single procedure.
 | External Transport Symbols | Appears on External Transport Cassettes to indicate Cassette can be used during patient transfer in rescue vehicle, fixed wing, or helicopter.
 | Ingression | Code for the level of ingression protection tested. The enclosure was tested to be drip proof.
 | Magnetic Resonance (MR) Conditional | Indicates that the System has been demonstrated to pose no known hazards in a specified MRI environment with specified conditions of use.
 | Manual Ventilation | Output port for GENOSYL to manual ventilation system
 | Manufacturer | Indicates the manufacturer of the item.
 | NO Injection | Output port for GENOSYL to patient circuit
 | Operating Instructions | Refer to operating instructions for instructions for use, warnings, precautions, and other equipment information.
 | RF Interference | Devices marked with this symbol may interfere with the Console.
 | Sample Gas Inlet | Attachment point for Sample Line on Water Trap
 | Serial Number | Indicates the serial number so that a specific medical device can be identified.
 | Storage humidity range | Indicates the range of humidity to which the medical device can be safely exposed.
 | Storage temperature range | Indicates the temperature limits to which the medical device can be safely exposed.
 | Unlock position | Direction to push to open the Water Trap.
 | Use by | Indicates the date after which the medical device is not to be used.
 | Water Trap Attachment Point | Indicates the location where the Water Trap with Sample Port is to be attached.

GENOSYL DS PARTS / COMPONENTS

PART

PART NAME

GENOSYL DS Cart

GENOSYL DS Console
(2 required per System)

MR Conditional GENOSYL DS System

Gauss Alarms Mount
(2 gauss alarms installed)

External Transport Mount

External Transport Mount with Quick Connect Plate

Adaptive Sensor Cable

The following parts are required to set up the GENOSYL DS and deliver nitric oxide to the patient breathing circuit, using validated ventilators, ventilator circuits, and manual ventilation equipment.

PART

PART NAME

GENOSYL Hospital Cassette
(may be referred to as Cassette or Hospital Cassette)

GENOSYL External Transport Cassette
(may be referred to as Cassette or External Transport Cassette)

Adaptive Sensor

NO Gas Injection Adapter
22M/15F × 22F

Adapter
22F × 22F

Inline Breathing Circuit Filter

.

GENOSYL DS Mixer

GENOSYL DS Gas Lines:
NO Injection Line (red)
Sample Line (blue)
Manual Ventilation Line (clear)

GENOSYL DS Sample Line Extension

Neonatal Gas Sample Tee

Water Trap

22M 22F Elbow Adapter

Sample Line Filter

Sample Tee, 3/8" Barbed

Injection Line Filter

22M/15F × 22M/15F Adapter

15M × 4.5 Adapter

22M/15F × 15M Gas Sample Tee

22F × 15M Adapter

Note: Physical appearances may vary slightly.

The following parts are required to deliver nitric oxide using a manual ventilation system.

PART

PART NAME

GENOSYL DS Manual Ventilation Bag NO Adapter

Note: Physical appearances may vary slightly.

The following parts are required for routine maintenance.

PART

PART NAME

Calibration Gas - 45 ppm NO

Calibration Gas - 10 ppm NO2

Calibration Regulator

Calibration Tee Tubing

Calibration Extension Tubing

Calibration Gas Carrying Case

Calibration Equipment Wrench

Calibration Regulator Teflon Washer

Note: Physical appearances may vary slightly.

GENOSYL®DS

SECTION 1
GENERAL INFORMATION

1. GENERAL INFORMATION

1.1 User Responsibility

The GENOSYL DS (Console) will perform as described in this Operator's Manual, accompanying inserts, and/or labels when assembled, operated, maintained, and repaired in accordance with the instructions provided. The Console must be set up as described in Section 3. If the Console does not perform as described in Section 3or during assembly, the parts are found to be broken, missing, contaminated, or visibly worn, they should be replaced immediately.

In the case of repair or replacement of the Console is required, a telephone service request should be made to Technical Support at 877-337-4118.The GENOSYL DS or any of its parts should not be serviced or repaired by anyone other than a VERO Biotech Technical Engineer or without written permission from VERO Biotech Technical Engineering Department.

Any malfunction resulting from faulty maintenance, improper repair, damage, alteration by anyone other than a VERO Biotech Technical Engineer, and/or improper use will be the sole responsibility of the User.

WARNING

The GENOSYL DS must only be used in accordance with the approved indications, usage, contraindications, precautions, and warnings described in the GENOSYL DS labeling. Refer to the labeling prior to use.

CAUTION

U.S. Federal law restricts this device to sale by or on the order of a physician. Outside the U.S., check local laws for any restrictions that may apply.

NOTES

- Prior to using the GENOSYL DS, read through this Operator's Manual.
- Follow all instructions and obey the Warnings and Cautions.
- Keep this Operator's Manual available to readily answer questions.
- Read through all manufacturer Operator's Manuals for the ventilator, humidifier and any other accessory items used.

1.2 General Information and Indications for Use

GENOSYL DS generates and delivers NO for inhalation at the point of use. The concentration of NO, as set by the user, is monitored, and adjusted to accurately dose the patient throughout an inspired breath. Only validated devices / components should be used with the GENOSYL DS.

The intended population for inhaled NO treatment is term and near-term neonates in neonatal intensive care units (NICUs). Refer to the GENOSYL (nitric oxide) for inhalation drug label for more detailed information.

The GENOSYL DS is intended for use in the hospital, 1.5 Tesla and 3.0 Tesla diagnostic imaging environments, during patient transfer via rescue vehicle, fixed wing aircraft, or helicopter, and the operating room in conjunction with validated anesthesia gas machines.

The GENOSYL DS is intended for use by healthcare professionals (HCPs) who are licensed and actively practicing pediatric and/or neonatal respiratory therapists (RTs), or HCPs in the operating room with the supervision of RTs in the United States. These users are required to set up, administer inhaled nitric oxide (iNO) and provide respiratory care (including initiation and maintenance of mechanical ventilators) in the critically ill neonatal population.

The GENOSYL DS starts with liquid N2O4/NO2, which is then converted in a proprietary Cassette to NO. The GENOSYL DS delivers NO into the ventilator stream, where the NO joins a stream of air or O2and is diluted to the prescribed concentration.

The NO concentration (dose) to be delivered to the patient is selected by the user and is set and maintained independently by means of computer-controlled air pumps, Cassette heaters, and a feedback loop that measures the delivered NO concentration.

The GENOSYL DS takes a gas sample removed from the NO gas flow stream immediately prior to the patient and provides real-time output of the NO, NO2, and O2concentrations that are being delivered to the patient. The continuous integrated gas monitoring includes a comprehensive alarm system.

The NO concentration detected from the sample line is used in a feedback loop to adjust the NO concentration delivered into the ventilator circuit.

The GENOSYL DS includes a redundant Console for complete back-up capability for delivery of NO for inhalation. Each Console has a back-up battery that is expected to last up to four hours under optimal conditions in the absence of an external power source. Console will alarm when less than 15 minutes of battery life remains.

1.3 Principles of Operation

GENOSYL DS. The GENOSYL DS continuously introduces a precisely controlled concentration of nitric oxide (NO) into the inspiratory limb of the ventilator circuit. GENOSYL DS utilizes the known properties of NO and other oxides of nitrogen, namely dinitrogen tetroxide (N2O4) and nitrogen dioxide (NO2), to create a "tankless" drug/device combination System to produce, at the point of use, ultra-high purity NO for inhalation, providing a consistent, prescribed dose to the patient.

Console.The GENOSYL DS Console contains the electronics to control the production and to maintain the constant and precise delivery of NO.

The primary features of the Console front panel are displayed in Figure 1.

NO generation.The Console uses Cassettes containing liquid N2O4/NO2inside a stainless-steel vessel (the liquid module) and an antioxidant cartridge. Upon initiation of a Cassette, the liquid N2O4is heated, producing NO2gas, which is mixed with up to 0.9 LPM ambient air supplied by the Console. The NO2/air is injected into the antioxidant cartridge inside the Cassette, which converts NO2to NO.

The Cassette is designed to provide NO in concentrations up to 80 ppm. The maximum and minimum delivered dose for a range of constant inspiratory flow rates is presented in Figure 2.

The maximum combination of dose (ppm) and flow (LPM) output of the System is 800 ppm × LPM (e.g., 20 ppm with 40 LPM, 40 ppm at 20 LPM, etc.). The System is capable of delivering NO at a minimum of 1 ppm × LPM (e.g., 1 ppm at 1 LPM).

The total time to deplete the Cassette N2O4contents depends on the rate of use. The minimum time to depletion based on use rate for Hospital Cassettes is shown in Figure 3.The minimum time to depletion of the External Transport Cassette based on use rate is shown in Figure 4.The calculated minimum remaining contents at the current output rate is indicated by a gauge presented on the Console display during use.

NO Injection into the Ventilator Circuit. After NO is produced in the Cassette, the NO injector introduces the concentrated NO into the ventilator circuit where the NO is diluted to the prescribed concentration (dose) and mixed with the O2or air supplied to the patient.

GENOSYL Smart Feedback System™Before the gas mixture reaches the patient, a sample line removes a small gas sample and sends it back to the Console, where gas sensors continuously measure the supplied NO, NO2and O2. The Console software then compares the measured NO concentration to the set NO concentration and continuously adjusts the delivery of NO to maintain the prescribed NO concentration (dose) delivered to the patient (closed loop control). The Console software commands the NO injection flow rate into the ventilator circuit with a maximum flow rate of 0.9 LPM. Changes in the ventilator settings by the user may cause brief transient changes in the measured NO value. The Console software will adjust the injected flow rate and the internal temperature of the Cassette to compensate for the changes in the total ventilator flow rate. For example, a higher minute ventilation will require a higher injection flow rate to produce the same NO concentration.

Mixer. An inline Mixer is used in the applicable ventilator circuit after the NO injection site and before the gas sample site to mix NO from the Console with the gas supplied by the ventilator, for specific ventilator and tidal volume use cases per Section 12.2.

Gas Monitoring.The gas mixture delivered to the patient by the GENOSYL DS is continuously monitored with two NO detectors, with one providing redundant back-up, as well as a detector for NO2and O2. A sample of inspired gas is taken from the inspiratory limb, close to the patient, and is measured by the gas sensor within the Console. The gas monitoring sensors are electrochemical; they are specific to each gas and provide an electronic signal that is proportional to the concentration of gas present.

Adaptive Sensor.The Adaptive Sensor is used to detect flow in the patient breathing circuit. When flow is not detected by the Adaptive Sensor, nitric oxide delivery will be interrupted until flow is detected. The Console will provide a visual and audible low priority alarm when flow is not detected to alert the user (see Section 10.5). Once flow is detected, the Console will auto resume delivery of nitric oxide at the previously set dose. An Adaptive Sensor is recommended for use with certain breathing devices. Refer to Section 3for recommended set up diagrams. The GENOSYL DS will properly deliver and control nitric oxide dose in the absence of an Adaptive Sensor.

Alarms and Dosing Safeguard Fallback Modes.The GENOSYL DS alerts the user in the event of excursions of NO, NO2, and Oxygen from their expected ranges. Nitric oxide delivery interruption conditions are as follows:

1. NO > 100 ppm
2. NO2reaches 3 ppm
3. The measured respiratory circuit dilution flow drops below 0.3 LPM as measured by the Adaptive Sensor.

The Console will provide a visual and audible high priority alarm. When detecting a sustained gas level higher than the above limits for 11 consecutive seconds, the Console will interrupt delivery of NO until the sampled levels of NO and/or NO2decrease to a safe level. Once sampled levels are in acceptable range, the Console will resume delivery with previously set dose.

If the cause of the high gas cannot be resolved, the use of the Back-up Console may be required. Refer to Section 10.1for additional information on alarms and dosing safeguards.

If NO delivery was interrupted due to the GENOSYL DS Adaptive Sensor reading dropping below 0.3 LPM, the Console will resume delivery with the previously set dose once the Adaptive Sensor reading exceeds 0.35 LPM. The automatic resumption of dose delivery after the interruption conditions listed above are cleared is one of the safety fallback modes of the GENOSYL DS.

Back-up NO Delivery.The Back-up Console is used to administer nitric oxide when the Dosing Console cannot be used. This Console has a separate power supply, and at least one Cassette loaded and preheated. If the Dosing Console fails to deliver NO, the Back-up Console is ready to begin dosing to continue NO delivery.

Transition to a new Cassette.When a Cassette approaches depletion, the Dosing Console will automatically transition to the second Cassette in the Console. Once the dosing Cassette is depleted, the Dosing Console will eject the depleted Cassette and alert the user to replace via the Cassette Status Indicator.

Disposal of the Cassette. Following use, any remaining Cassette contents are purged into an inerting chamber, where the contents are chemically neutralized, rendering the Cassette safe for disposal.

1.4 Exposure of Healthcare Providers to NO and NO2

Occupational exposure of healthcare providers to NO or NO2may occur during Inhaled NO therapy for patients. Below are examples of calculated and observed exposure to NO or NO2, in the context of guideline workplace exposure limits.

Calculated and observational methods show that the exposure levels to NO or NO2from an NO delivery system are significantly less than the levels recommended by the National Institute for Occupational Safety and Health (NIOSH).

Workplace Limits: NIOSH has recommended workplace exposure limits as follows [NIOSH Pocket Guide to Chemical Hazards, Dept of Health & Human Services, Centers for Disease Control and Prevention, National Inst for Occupational Safety & Health. Publication 2005-149, Sept 2007.] .

NO | time-weighted (8 hours) average concentration limit of 25 ppm
NO2 | Recommended exposure limit of 1 ppm

Theoretical Calculation.The build-up of NO in a well-ventilated ICU room, with NO flowing directly into the room, can be evaluated using the following calculation:

Room size | 1000 ft^3
Room volume | 28,300 L
Room ventilation (6 complete exchanges/hour) | 2,830 L/min
NO flow into the room | 80 ppm at 14 L/min
Average NO room concentration | 0.4 ppm of NO

Observations of NO Exposure. The theoretical calculation has been supplemented by actual measurements in three independent studies in actual therapeutic use settings. [Hess et al, Use of Inhaled Nitric Oxide in patients with Acute Respiratory Distress Syndrome. Respiratory Care 1996; 41(5):424-446.] , [Phillips M, Hall TA, Sekar K, Tomey JL. Assessment of Medical Personnel Exposure to Nitrogen Oxides During Inhaled Nitric Oxide Treatment of neonatal and Pediatric Patients. Pediatrics. 1999;104(5):1095-1110.] , [Qureshi MA, Shah NJ, Hemmen CW, Thill MC, Kruse JA.Exposure of Intensive Care Nurses to Nitric Oxide and Nitrogen Dioxide during Therapeutic use of Inhaled Nitric Oxide in Adults with Acute Respiratory Distress Syndrome. Am. J. Crit Care, 2003;12(2):147-153.] The studies found that detectable exposures to NO and NO2were brief, infrequent, and well below recommended exposure limits.

If the location for using NO has uncertain ventilation, then the location should be evaluated for NO and NO2build-up prior to use.

GENOSYL®DS

SECTION 2
SYSTEM OVERVIEW

2. SYSTEM OVERVIEW

2.1 Frequently Used Functions

Detailed instructions are provided in this manual for the primary user interaction and frequently used functions of the GENOSYL DS, which include:

System Set-Up and Connections (Section 3)

- Connections to Various Breathing Systems
- GENOSYL DS Ventilator Circuit Assembly Pre-Check
- GENOSYL DS Injection Assembly with Adaptive Sensor
- GENOSYL DS Mixer Assembly with Adaptive Sensor
- GENOSYL DS Console Connections
- GENOSYL DS Gas Line Connections
- GENOSYL DS Sample Line Extension Connection
- GENOSYL DS Adaptive Sensor Cable Connection
- GENOSYL DS Ventilator Circuit Connection
- GENOSYL DS Manual Ventilation Connections
- GENOSYL DS Mechanical Ventilator Circuit Connections
- Gas Sampling During Aerosol Delivery

System Start-Up (Section 4)

- Console Start-Up
- Cassette Insertion
- Water Trap / Sample Line Leak Test

Nitric Oxide Administration (Section 5)

- Setting a Dose when using a Circuit with an Adaptive Sensor
- Setting a Dose when using a Circuit without an Adaptive Sensor
- Adjusting the Dose
- Manual Dosing Mode
  - Manual Ventilation Use (Bagging)
  - Preset Manual Dosing Mode Flow Rate (Optional)
  - Resuming Primary Dosing
- Console Use as Back-up

Console Shutdown (Section 6)

- Console Shutdown
- Cassette Removal
- Cassette Disposal

Using the System in the MR Scanner Room (Section 7)

- Connection to the Ventilator Circuit
- Transferring to and from the MR Scanner Room

External Transport (Section 8)

- External Transport Set-up and Ventilator Circuit Schematics
- Using GENOSYL DS for External Transport

Use with an Anesthesia Gas Machine (Section 9)

- Connection to a Dual Limb Anesthesia Circuit
- Connection instructions for the GENOSYL DS to an Anesthesia Gas Machine

Alarms, Alerts, and Troubleshooting (Section 10)

- On-Screen Troubleshooting Module
- Alarms (High, Medium, and Low Priority)
- Informational messages
- GaussAlert™ Alarm
- Troubleshooting
- Leak Detection Tool

System Maintenance (Section 11)

- Calibration
- Maintenance Schedule
- Testing the GaussAlert™ Function
- Water Trap Maintenance
- Battery
- Cleaning
- Storage

2.2 GENOSYL DS Cart and Consoles

The following pages contain photos of the GENOSYL DS Consoles. The specific sections of the GENOSYL DS are numbered with the respective description listed below the photo.

WARNING

- NEVER use the MR Unsafe GENOSYL DS Cart in the MR scanner room.
- ALWAYS verify at least one gauss alarm is functioning properly prior to use in the MR environment.

CAUTION

- ALWAYS operate the Console on a level surface to avoid potential interruption to nitric oxide (NO) delivery.
- DO NOT stand or sit on the Cart. Standing or sitting on the Cart can damage device.
- ALWAYS push or pull the Cart using the handle only. NOT doing so may result in damage to the device.

NOTE

A System has a top and bottom Console. Both Consoles will start-up in Primary Dosing Mode. One Console will be used for dosing and the other will remain in Primary Dosing Mode as a Back-up Console. (See Section 5.5)

2.3 Cassette

The Cassette contains the material that will be converted to nitric oxide during the activation process. It is inserted into the GENOSYL DS Console, and its shape helps ensure proper orientation during the insertion process. A Cassette State Window is located on the front of the Cassette to indicate if the Cassette is available for use (blue), or if it has been inerted and unavailable for use (bleached and reddened).

The GENOSYL DS requires different Cassettes for use in the hospital (ICU or MR setting of care) and for use in external patient transport. The Hospital Cassette is blue in color. See Figure 12for details about the Hospital Cassette. The External Transport Cassette is orange in color. Refer to Section 8for more information about using the GENOSYL DS in external transport and Figure 13for details about the External Transport Cassette.

Cassette in Packaging

Unused Cassette

Inerted Cassette

Figure 12: GENOSYL Cassette

External Transport Cassette in Packaging

Unused External Transport Cassette

Inerted External Transport Cassette

Figure 13: GENOSYL External Transport Cassette

CAUTION

DO NOT remove Cassette from packaging until ready to use. External packaging is designed to protect the Cassette from damage and/or contamination.

2.4 GENOSYL DS Ventilator Circuit Components

The following parts are used to set up the GENOSYL DS portion of the patient respiratory circuit, as specified in Section 3.2.

PART | PART NAME | FUNCTION
 | Adaptive Sensor | Used to measure flow from the ventilator into the circuit.
 | Adaptive Sensor Cable | Used to communicate flow readings to the Console.
 | GENOSYL DS Gas Lines NO Injection Line (red) Sample Line (blue) NO Manual Ventilation Line (clear) | Used to deliver nitric oxide to the ventilator circuit and manual ventilation bag, and to sample gas within the ventilator circuit.
 | GENOSYL DS Manual Ventilation Bag NO Adapter | Used to connect oxygen tubing to manual ventilation bagging system to deliver nitric oxide. Includes an NO Injection Port to connect to the NO Injection Line.
 | GENOSYL DS Mixer | Used to mix the NO gas with the gas supplied by the ventilator through a filter containing silica gel to provide intra-breath NO delivery for certain scenarios.
 | Adapter 22F × 22F | Used as a coupler between the Mixer and the Gas Injection Adapter when a Mixer is required.
 | GENOSYL DS Sample Line Extension | Used when the distance between the patient and the DS exceeds the length of the standard sample gas line in the MR Environment.
 | Injection Line Filter | Used to filter air from the Injection Line.
 | Inline Breathing Circuit Filter | Used to filter air from the Injection Line, and on the expiratory limb when used with an anesthesia gas machine.
 | Neonatal Gas Sample Tee | Used to connect the Sample Line to the ventilator circuit.
 | NO Gas Injection Adapter 22M/15F × 22F | Used between the Adaptive Sensor and the Inline Breathing Circuit Filter, and to connect to the NO Injection Line (red).
 | Sample Tee, 3/8" Barbed | Used to accommodate gas sampling in some ventilator circuits, (e.g., Crossvent Infant Circuit).
 | Sample Line Filter | Used to protect sampling system during use with aerosol medications (refer to Section 3.8).
 | Water Trap | Used to protect sample system by collecting condensation and filtering contaminants from the sampled gas. The Water Trap may need to be emptied or changed while in use (refer to Section 11.4).
 | 22M/15F × 22M/15F Adapter | Used to create GENOSYL DS sampling port 6 to 12 inches from the patient wye.
 | 15M × 4.5 Adapter | Used between Oxygen Tubing and NO Gas Injection Adapter with some non-invasive gas delivery systems.
 | 22M/15F × 15M Gas Sample Tee | Used to connect the Sample Line to the ventilator circuit.
 | 22F × 15M Adapter | Used to assist with connection of the NO Delivery Injection Assembly to various ventilator circuits.

2.5 Gas Lines (detailed explanation)

Gas lines are used to deliver nitric oxide from the GENOSYL DS Consoles to the ventilator circuit and manual ventilation bag, and to sample gas within the ventilator circuit. The lines are color coded and labeled with icons corresponding to colors and icons on each Console.

The NO Injection Line (red) delivers nitric oxide from the Console to the mechanical ventilation circuit (described in Section 3.5).

The Sample Line (blue) also contains a stopcock to conduct the Water Trap / Sample Line Leak Test (described in Section 4.2).

A Sample Line Extension is available when additional distance between the patient circuit and the Console is required (e.g., use in the MR environment) (described in Section 3.5.2).

The Manual Ventilation Line (clear) delivers nitric oxide from the Console to the Manual Ventilation Bag NO adapter (described in Section 3.6).

2.6 Console Dosing Modes of Operation

During operation, a Console can be in one of two dosing modes; Primary Dosing Modeor Manual Dosing Mode. The user can switch the dosing modes during normal operation to perform specific functions for certain conditions. The following table summarizes key characteristics of each dosing mode. Both dosing modes are available when External Transport is ON and when External Transport is OFF.

MODE | FUNCTIONAL CHARACTERISTICS
Primary Dosing | - The dosing mode of operation for controlled dosing with Smart Feedback System™.
Manual Dosing | - The dosing mode of operation used for manual ventilation. - Manually adjustable fixed dosing without the need of feedback for certain conditions.

2.7 Display Screen

The GENOSYL DS display screen is presented below (Figure 15) followed by a table with descriptive text corresponding to the numbers shown around the display screen.

NOTE

Some confirmation display screens (e.g., "Confirm", "Yes", "Accept", etc.) will be semi-transparent after dosing has been initiated to allow the Operator to continue to see important information on the underlying screen (e.g., NO values, Alarms, Alerts, etc.).

2.8 Display "Menu" Tab Navigation

The table below consists of the available "Menu" tabs (Main, Alarms, Calibration, Events, and Settings) along with the functional description of each tab, and the buttons within each tab. When regular night (dark) display view is used and a tab is selected, the title of the tab will appear on a bright blue background. When the tab is not selected, it will appear with a dark blue background. When day (light) display view is used, and a tab is selected, the tab will appear on a bright blue background. When the tab is not selected, it will appear on a light blue background. When External Transport Mode is ON, the tab currently selected will have an orange background and tabs not actively selected will have a blue background.

MENU TAB DISPLAY

TAB / BUTTON

DESCRIPTION

Press this tab to access the sub-level tabs (Main, Alarms, Calibration, Events, and Settings).

Displayed when the "Alarms" tab is selected, this screen is used to set the Upper and Lower Alarm Limits for NO (ppm), NO2(ppm), and O2(%).
A list of Alarms that have occurred since the last reset for the Console will be displayed on this tab.

NOTE

See Section 10for additional information on alarms and alerts.

Displayed after pressing the "Alarms" tab, press this button to switch to the default upper and lower limits for NO (ppm), NO2(ppm), and O2(%).

Pressing this button will clear the alarm history from the alarm log visible on this tab. The alarm will remain logged in the Console's permanent logs.

Press this tab to return to the main screen. Pressing the Main Tab will collapse the tab menu.

Press this tab to access the calibration screen.

NOTE

See Section 11.1for additional information on Calibration.

Press this button to calibrate the low range of the NO and NO2sensor.

Press this button to calibrate the high range for the NO sensor.

Press this button to calibrate the high range for the NO2sensor.

Press this button to initiate calibration for the selected gas.

Press this button to stop the calibration in the middle of a calibration process. The previous calibration will remain to be used.

Press this button to display the history of calibration.

Press this tab to access the events menu.

Press this button to clear the events listed on the events screen.

Press this tab to access the settings screen.

Press this button to begin the process of shutting down the Console.

Press this button to switch display to day (light) display view. This will switch the display to a lighter gray background instead of the dark blue background.

This drop-down menu allows operator to preset the dilution flow rate for Manual Mode. If no rate is selected, Console will default to 10 LPM.

Press this button to enter the screen to adjust the date and time. This button is only present when logged in as an Administrator

Press this button to adjust the date and time. This button is only present when logged in as an Administrator

Press this button to perform a "Water Trap/ Sample Line Leak Test".

Used by service personnel only. Password controlled.

NOTE

Contact Technical Support at 877-337-4118for additional support.

Press this button to display a window to enter date ranges to retrieve dosing usage over a period of time and number of Cassette activations.

Press this button to enable External Transport Mode. This button is gray when External Transport Mode is OFF.

NOTE

This will require the transport PIN. Contact Technical Support for additional support.

Press this button to disable External Transport Mode. This button is orange when External Transport Mode is ON.

NOTE

This will require the transport PIN. Contact Technical Support for additional support.

When External Transport Mode is ON, the External Transport animated icons will rotate between these three icons in the upper right corner of the screen next to the Alarm icon.

Day (Light) display view Main Menu: Press this tab to access the sub-level tabs (Main, Alarms, Calibration, Events, and Settings).

Press this button to switch display to regular night (dark) display view. This button is located on the "Settings" tab.

2.9 Display Screen Operational Buttons

The following buttons on the display screens allow the Operator to operate and adjust the GENOSYL DS prior to and during the delivery of nitric oxide.

Note: the following are shown in regular night (dark) display view but are also available in day (light) display view.

BUTTON

DESCRIPTION

Press this button to set the targeted NO (ppm) dose when in Primary Dosing Mode.

Press this button to pre-silence alarms. Pushing this button will pre-silence specific alarms for 120 seconds.
When active, a red "X" will appear through the alarm icon with a countdown of how much longer alarms will be pre-silenced for. When tapping the icon with the red "X", the user will cancel the pre-silence.

Press this button to cancel the Water Trap / Sample Line Leak Test.

Press this button to switch a Console to Primary Dosing Mode from Manual Dosing Mode.
When in Primary Dosing Mode, the dosage can be set to a user selected (prescribed) level.

Press this button to switch from Primary Dosing Mode to Manual Dosing Mode.
See Section 5.4for information about dosing in Manual Dosing Mode.

Electronic keypad used to set and adjust the prescribed targeted nitric oxide dose to be delivered to the patient. Includes buttons to confirm "OK", "Cancel", or "Clear" the entry.

The Total Flow range is selected by the user if the Adaptive Sensor is not connected to the Console. These buttons will only appear if the Console does not detect an Adaptive Sensor when setting or adjusting dose.
Total Flow range is the sum of the ventilator (or ancillary equipment) Bias Flow and the minute ventilation of the patient.

Displayed when in Manual Dosing Mode, press the green up or down arrows to adjust the dose to the patient, from the default dose.
Pressing the down arrow will decrease the dose in increments of 1 ppm for 24 ppm and below. Pressing the up arrow will increase the dose in increments of 2 ppm above 24 ppm.
Press the green LPM (liters per minute) button to activate a drop-down menu and set a different dilution flow rate.

Press this button to confirm the action specified on the screen.

Press this button to cancel the action specified on the screen.

Press this button to acknowledge the information message displayed on the screen.

Press this button to move to the next step.

Press this button to cancel the current step.

2.10 Display Screen – Cassette Status Indicators

The following describes the Cassette Status Indicators that will be shown on the display screen prior to, during, and post-delivery of nitric oxide. The Cassette Status Indicators consist of two Cassette icons, which correspond to the left and right Cassette receptacles.

CASSETTE STATUS
INDICATOR DISPLAY

DESCRIPTION

This Cassette Status Indicator will be displayed when a Cassette is not loaded into the Console. The Cassette Status Indicator will display "REPLACE" and will alternate between a dark red and light red.
The user is prompted to "Replace"

This Cassette Status Indicator is displayed during the warmup phase when a new Cassette is inserted. This indicator will display "WARMING" alternating with "READY". Dose may be initiated while the Cassette is warming.

This Cassette Status Indicator is displayed once the Cassette has achieved a fully preheated status.

This Cassette Status Indicator is displayed during dosing.
If a secondary Cassette has been inserted, the Cassette Status Indicator will display "Dosing" for the dosing Cassette and "Ready" for the secondary Cassette.
If a secondary Cassette has not been inserted, the Cassette Status Indicator will display the percentage of nitric oxide remaining in the dosing Cassette and the secondary Cassette Status Indicator will be red and display "Replace". A low priority tone will also sound in ten second intervals until a secondary Cassette is inserted.

This Cassette Status Indicator will be displayed when the Console is transitioning from the dosing Cassette to the secondary Cassette. The direction of the arrow indicates the Cassette that is being transitioned to.

This Cassette Status Indicator will be displayed when less than one hour of Cassette life remains and no secondary Cassette is inserted. The indicator will display the percentage of life remaining in the dosing Cassette and the estimated time before depletion.
The Cassette Status Indicator for the dosing Cassette will appear yellow and display "Dosing" and the other Cassette Status Indicator will appear red and display "Replace"

This Cassette Status Indicator is displayed when a Cassette is depleted and no secondary Cassette is inserted in the Console. This status will only display if another Cassette is not present in the Console.
The Cassette Status Indicator for the dosing Cassette will appear red and display "Dosing 0%" and "0m". The empty Cassette Status Indicator will appear red and display "Replace". Both indicators will alternate between a dark and light red color.

This Cassette Status Indicator will be displayed when a Cassette that has previously been used is inserted in a Console. The Cassette display will alternate between "USED" and an "X" through the Cassette icon. The Console will automatically eject a previously used Cassette.

This Cassette Status Indicator will be displayed two minutes after inserting one Cassette into the Back-up Console. The secondary Cassette Status Indicator on the screen will switch from a red flashing "REPLACE" to an empty gray Cassette outline.
Once a dose is entered, and the inserted Cassette is activated, the outline will switch back to the red flashing "REPLACE" so the user is prompted to insert a secondary Cassette in the dosing Console.

This Cassette Status Indicator is displayed when a Cassette is non-operational. A white X will appear over a red Cassette Status Indicator. The Console will eject a non-operational Cassette and dose from the secondary Cassette, if properly inserted. User will be prompted to replace Cassette after ejection.

This Cassette Status Indicator is displayed when a Cassette is past its expiration date. The display will read "EXPIRED". An expired Cassette cannot be used for dosing and will be automatically ejected from the Console. User will then be prompted to replace the ejected Cassette via the Cassette Status Indicator.

This Cassette Status Indicator will be displayed when the wrong Cassette type is inserted into the Console. The display will read "WRONG TYPE" then proceed to eject the incorrect Cassette from the Console.
A Hospital Cassette will be ejected while External Transport Mode is turned ON and an External Transport Cassette will be ejected while External Transport Mode is turned OFF.

2.11 Display Screen - Adaptive Sensor Status

The following describes the Adaptive Sensor status that will be shown on the display screen. The Adaptive Sensor Icon is located on the top left of the Console display screen. To troubleshoot the Adaptive Sensor, see Section 10.8 Troubleshooting.

ADAPTIVE SENSOR DISPLAY

DESCRIPTION

The Console has detected flow through the Adaptive Sensor.

The Console has detected an Adaptive Sensor without flow.
To initiate delivery, the Console requires flow detection. The Set button will not appear until flow is detected through the Adaptive Sensor. The screen will appear as pictured below. Once flow is detected, the "Set" button will appear and allow the user to set the dose.
If the Adaptive Sensor stops detecting flow while dosing, the Console will interrupt delivery of NO into the circuit and display a turquoise "Flow Not Detected-Nitric Oxide Delivery Interrupted" message. This message will be accompanied by a low tone every 10 seconds. See Section 10.5 Low Priority Alarms and Messages.

The Console does not detect an Adaptive Sensor is connected

An Adaptive Sensor is detected but the Adaptive Sensor is either malfunctioning or not properly connected to the Adaptive Sensor Cable.

2.12 Cassette Insertion into Console

WARNING

ONLY use External Transport Cassettes, identified by orange color and transport sticker, in external transport outside of the hospital.

When inserting a Cassette into a Console, it is important to push the Cassette fully into the receptacle and confirm the Cassette has been registered on the screen.

PHOTO

DESCRIPTION

Insert the Cassette into the receptacle. Push in until you hear the Cassette click into the mechanism.

The on-screen Cassette Status Indicator will switch to say "READY" and then prompt the user to begin a Water Trap/ Sample Line Leak Test.

2.13 Water Trap / Sample Line Leak Test

A Water Trap / Sample Line Leak Test is initiated when a Cassette has been inserted into the Console and fully seated, and if the measured NO is less than 1.0 ppm. Its purpose is to test the integrity of the Water Trap seal, the proper seating of the Water Trap, and the Sample Line connection to each Console, prior to operation. This is important to ensure an accurate measurement of NO within the ventilator circuit.

After the test has been initiated, the screen will prompt the Operator to close the Stopcock Valve and the Operator will have 60 seconds within which to do this. A numerical timer and a horizontal progress bar provide a visual representation of the time elapsed (red) and time remaining (gray). Once the Stopcock Valve has been closed and if the test has been successfully completed, the entire progress bar will turn green.

TEST IN PROCESS

TEST PASSED

Figure 16: Water Trap / Sample Line Leak Test

If the test has failed, the progress bar will remain red throughout the full 60 seconds. The Operator will be notified and prompted to troubleshoot the potential cause

Prior to completion of the leak test and if a condition exists in which immediate NO delivery is required, the Operator may cancel the leak test. The GENOSYL DS will allow a dose of 20 ppm to be set in Primary Dosing Mode. If a different dose is required, a Water Trap /Sample Line Leak Test must be completed.

The Water Trap / Sample Line Leak Test may also be initiated manually via the "Settings" tab and pressing the "Perform Leak Test" button. This may be useful to test the integrity of the Water Trap and Sample Line independent of the need to initiate the delivery of nitric oxide (see Settings in Section 2.8).

2.14 Console Shutdown - Cassette Status Indicator

The following describes the Cassette Status Indicators that will be shown on the display screen as the Console is shutting down. For proper Console shutdown procedures, see Section 6.

CASSETTE STATUS INDICATOR

DESCRIPTION

This Cassette Status Indicator will display "SAVE" on the shutdown screen to note which Cassette should be retained for future use. This Cassette has not been activated for dosing.

This Cassette Status Indicator will display "DISPOSE" on the shutdown screen to note which Cassette should be disposed of per hospital policy.
This Cassette was used for dosing or has been activated.

This Cassette Status Indicator will appear on the shutdown screen to note no Cassette was inserted into the receptacle.

2.15 Battery Charge Status Indicator

CHARGE STATUS INDICATOR | DESCRIPTION
Solid Red | Battery Power Supply Error. See Battery Error Alarm in Section 10.3.
Blinking Red | Communication Failure or Hardware Error. See Hardware Failure Alarm in Section 10.3.
Solid Amber | Console is unplugged and using battery power. See System is running on low Battery Alarm in Section 10.5.
Blinking Amber | Console is using battery power and running on low battery. See Low Battery Alarm in Section 10.5.
Solid Green | Console is plugged in and battery is fully charged.
Blinking Green | Console is plugged in and the battery is charging.

GENOSYL®DS

SECTION 3
SYSTEM SET-UP AND CONNECTIONS

3. SYSTEM SET-UP AND CONNECTIONS

3.1 GENOSYL DS Set-Up and Mechanical Ventilator Circuit Schematic

NOTE

Naming conventions: The GENOSYL DS accessories and components consist of the GENOSYL DS Injection Assembly with Adaptive Sensor, (Section 3.4.1), or the GENOSYL DS Mixer Assembly with Adaptive Sensor (Section 3.4.2), and the GENOSYL DS Gas Lines (Section 3.5). Refer to Section 12.2 Table 15for when use of the Mixer Assembly with Adaptive Sensor is recommended. Connections and disposable circuits to breathing systems may vary and are unique to individual manufacturers. Example circuit diagrams are provided for reference.

The schematic in Figure 17shows an example ventilator circuit set-up and connection to the GENOSYL DS, and a manual ventilation bagging system.

All required GENOSYL DS Parts / Components are listed in the front of this manual and should be removed from their packaging prior to set-up.

3.2 Connections to Various Breathing Systems

WARNING

- ALWAYS use the GENOSYL DS in accordance with the indications, usage, contraindications, warnings, and precautions described in the GENOSYL prescribing information and labeling. Refer to latest approved prescribing information and labeling prior to use.
- The approved patient population for the GENOSYL DS as specified in the drug labeling for GENOSYL (nitric oxide) for inhalation, is limited to neonates. The GENOSYL DS is not intended to be used in other patient populations.
- ONLY use the GENOSYL DS, its parts, and accessories as instructed. Using non-specified components may result in product malfunction, injury or death.
- ALWAYS follow pre-use setup instructions for the routing and connections of tubing to avoid patient strangulation.
- MAKE SURE the System has all tubing connected as described in the instructions. Not connecting all tubing may result in inaccurate dosage and harm to the patient.
- DO NOT use accessories or cables other than those specified or provided by the manufacturer of this equipment, as this may result in increased electromagnetic emissions or decreased electromagnetic immunity of this equipment and result in improper operation.

CAUTION

Prolonged use in dry environments without humidification will damage the gas sensors. Supplemental humidification providing greater than 20% relative humidity (RH) in the patient circuit is recommended.

NOTE

- All circuit components, including GENOSYL DS circuit components, should be changed out and disposed of according to hospital protocol.
- Refer to Section 8for use of the GENOSYL DS with an external transport ventilation device.
- Refer to Section 9for use of the GENOSYL DS with an anesthesia gas machine.

3.2.1 Conventional Ventilators

Compatibility testing has demonstrated performance meeting requirements for the GENOSYL DS operating range of 0 to 80 ppm with the following conventional ventilators at the operating ranges shown in Table 1.For further information on the use of the GENOSYL DS with validated MR conditional ventilators in the MR environment, refer to Section 7. For further information on the use of the GENOSYL DS with validated external transport ventilators, refer to Section 8. For use with validated anesthesia gas machine, see Section 9. See Section 12.2 Table 14for modes validated for each conventional ventilator. Validated ventilators were not tested with a nebulizer.

- Bio-Med Devices CrossVent 2+
- Bio-Med Devices MVP-10
- Dräger V500
- Dräger VN500
- Dräger V600
- Dräger VN600
- Dräger V800
- Dräger VN800
- Hamilton C1/T1
- Hamilton C6
- Hamilton G5
- Hamilton MR1
- Puritan Bennett 980
- Vyaire AVEA

WARNING

- ALWAYS ensure the trigger sensitivity of the ventilator is checked after connecting the GENOSYL DS to the breathing circuit or when the dose is changed. The GENOSYL DS injects and samples gas from the patient respiratory circuit which may affect the triggering sensitivity of the ventilator.
- ALWAYS ensure the patient disconnect and high–pressure alarms are used with the ventilator.
- ONLY use the GENOSYL DS with Bio-Med Crossvent 2+ with Constant Flow ON. Not doing so may lead to elevated NO2levels or dose variability.

CAUTION

- When using spontaneousbreathing modes on respiratory device, NO2levels may exceed 3.0 ppm when dosing ≥ 57 ppm NO into 100% FiO2and maximum bias flow, resulting in nitric oxide delivery interruption. Once sample value of NO2is below 3.0 ppm, the Console will auto resume delivery of NO at set dose. Refer to Section 12.1.5 Table 13for additional information.
- When using non-spontaneousbreathing modes on respiratory device, NO2levels may exceed 3.0 ppm when dosing ≥ 63 ppm NO into 100% FiO2and maximum bias flow, resulting in nitric oxide delivery interruption. Once sample value of NO2is below 3.0 ppm, the Console will auto resume delivery of NO at set dose. Refer to Section 12.1.5 Table 13for additional information.

NOTE

- If a higher than desired level of NO2is measured in the patient circuit, increasing respiratory device bias flow, if applicable, may result in decreased NO2levels.

Table 1: Conventional Ventilator Compatibility Test Ranges
Setting | Range | Unit
Inspiratory Flow Rate | 2-120 | LPM
Respiratory Rate | 6-60 | BPM
Peak Inspiratory Pressure | 0-70 | cmH2O
Positive End Expiratory Pressure | 0-20 | cmH2O

The ventilator circuit diagram for use withoutthe Inline Mixer accessory, required in certain scenarios, is shown in Figure 17. See Section 12.2, Table 15for applicable use scenarios.

The ventilator circuit diagram for use withthe Inline Mixer accessory, required in certain scenarios, is shown in Figure 18. See Section 12.2, Table 15for applicable use scenarios.

3.2.2 Non-Invasive Gas Delivery Systems

Compatibility testing has demonstrated performance meeting requirements for the GENOSYL DS operating range of 0 to 80 ppm with the following non-invasive gas delivery systems at operating ranges shown in Table 2.

- Fisher and Paykel Optiflow Jr 2 Breathing Circuit
- Fisher and Paykel Optiflow Breathing Circuit

Table 2: Non-Invasive Gas Delivery System Compatibility Test Ranges
Setting | Range | Unit
Optiflow Jr 2 Flow Rate | 0.5 - 25 | LPM
Optiflow Flow Rate | 5-60 | LPM

The Fisher and Paykel Optiflow Jr 2 Breathing Circuit for use with the GENOSYL DS is shown in Figure 19.

The Fisher and Paykel Optiflow Breathing Circuit for use with the GENOSYL DS is shown in Figure 20.

3.3 GENOSYL DS Ventilator Circuit Assembly Pre-Check

Follow the steps listed below for the initial System pre-check prior to completing the ventilator circuit assembly.

ILLUSTRATION | ACTION | Warnings, Cautions and Notes
- Cassettes– 3 ea. - Adaptive Sensor– 1 ea. - Adaptive Sensor Cable– 1 ea. - Gas Injection Adapter– 1 ea. - Inline Breathing Circuit Filter1ea. (2 Inline Breathing Circuit Filters will be needed for use with an AGM. Refer to Section 9for more information about use with an AGM) - Mixer Assembly - Mixer– 1 ea. - Adapter(22mm ID × 22mm ID) – 1ea. - Inline Breathing Circuit Filter– 1 ea. - Gas Lines– 1 ea. - Gas Sample Tee– 1 ea. - Manual Ventilation Bag NO Adapter– 1 ea. | 1. Removeall items of the GENOSYL DS Parts / Components from packaging. 2. Confirmthat the appropriate Cassettes for the intended use environment have been selected. 3. Checkthe expiration date for each Cassette and the Inline Breathing Circuit Filterto ensure use is within the expiration date. | WARNING
- Cassettes– 3 ea. - Adaptive Sensor– 1 ea. - Adaptive Sensor Cable– 1 ea. - Gas Injection Adapter– 1 ea. - Inline Breathing Circuit Filter1ea. (2 Inline Breathing Circuit Filters will be needed for use with an AGM. Refer to Section 9for more information about use with an AGM) - Mixer Assembly - Mixer– 1 ea. - Adapter(22mm ID × 22mm ID) – 1ea. - Inline Breathing Circuit Filter– 1 ea. - Gas Lines– 1 ea. - Gas Sample Tee– 1 ea. - Manual Ventilation Bag NO Adapter– 1 ea. | 1. Removeall items of the GENOSYL DS Parts / Components from packaging. 2. Confirmthat the appropriate Cassettes for the intended use environment have been selected. 3. Checkthe expiration date for each Cassette and the Inline Breathing Circuit Filterto ensure use is within the expiration date. | - DO NOT use a Cassette that is beyond its expiration date. Using an expired Cassette may affect the Cassette's ability to provide the correct NO dosage to the patient, which may cause injury or death. - ONLY use External Transport Cassettes, identified by orange color and transport sticker, in external transport outside of the hospital.
- Cassettes– 3 ea. - Adaptive Sensor– 1 ea. - Adaptive Sensor Cable– 1 ea. - Gas Injection Adapter– 1 ea. - Inline Breathing Circuit Filter1ea. (2 Inline Breathing Circuit Filters will be needed for use with an AGM. Refer to Section 9for more information about use with an AGM) - Mixer Assembly - Mixer– 1 ea. - Adapter(22mm ID × 22mm ID) – 1ea. - Inline Breathing Circuit Filter– 1 ea. - Gas Lines– 1 ea. - Gas Sample Tee– 1 ea. - Manual Ventilation Bag NO Adapter– 1 ea. | 1. Removeall items of the GENOSYL DS Parts / Components from packaging. 2. Confirmthat the appropriate Cassettes for the intended use environment have been selected. 3. Checkthe expiration date for each Cassette and the Inline Breathing Circuit Filterto ensure use is within the expiration date. | NOTE
- Cassettes– 3 ea. - Adaptive Sensor– 1 ea. - Adaptive Sensor Cable– 1 ea. - Gas Injection Adapter– 1 ea. - Inline Breathing Circuit Filter1ea. (2 Inline Breathing Circuit Filters will be needed for use with an AGM. Refer to Section 9for more information about use with an AGM) - Mixer Assembly - Mixer– 1 ea. - Adapter(22mm ID × 22mm ID) – 1ea. - Inline Breathing Circuit Filter– 1 ea. - Gas Lines– 1 ea. - Gas Sample Tee– 1 ea. - Manual Ventilation Bag NO Adapter– 1 ea. | 1. Removeall items of the GENOSYL DS Parts / Components from packaging. 2. Confirmthat the appropriate Cassettes for the intended use environment have been selected. 3. Checkthe expiration date for each Cassette and the Inline Breathing Circuit Filterto ensure use is within the expiration date. | A Mixer Assembly is not required for all use cases. Refer to Section 12.2, Table 15
 | 1. Visually inspectthe Water Traps on both Consolesto ensure they are installed and empty. | WARNING
 | 1. Visually inspectthe Water Traps on both Consolesto ensure they are installed and empty. | ALWAYS empty Water Trap before each use, when prompted by the System, and when the trap is more than half full. Allowing the Water Trap to completely fill will occlude the Sample Line which will interrupt patient gas NO, NO2, and O2concentration monitoring. Failure to monitor the patient gas NO, NO2, and O2concentrations may result in patient injury. ALWAYS conduct Water Trap / Sample Line Leak Test every time you empty and replace the Water Trap, as failure to do so may lead to an incorrect NO reading, which can result in injury or death.
 | 1. Visually inspectthe Water Traps on both Consolesto ensure they are installed and empty. | NOTE
 | 1. Visually inspectthe Water Traps on both Consolesto ensure they are installed and empty. | To empty the Water Trap, see Section 11.4.1.

3.4 Assembling GENOSYL DS Injection Assembly with Adaptive Sensor and GENOSYL DS Mixer Assembly with Adaptive Sensor

The Injection Assembly with Adaptive Sensor or the Mixer Assembly with Adaptive Sensor is the point of nitric oxide injection into the patient respiratory circuit. Only one type of assembly is required for each patient circuit. For certain scenarios, the Mixer Assembly with Adaptive Sensor is recommended to mix the NO gas with the gas supplied by the ventilator through a filter containing silica gel to provide intra-breath NO delivery. Refer to Section 12.2, Table 15for scenarios when a Mixer is recommended for use.

NOTE

When using a Mixer, an Inline Breathing Circuit Filter must be used. If a Mixer is not used, an Inline Breathing Circuit Filter as presented in Figure 21may be used, or an Injection Line Filter connected to the port on the Gas Injection Adapter may be used.

3.4.1 GENOSYL DS Injection Assembly with Adaptive Sensor

Follow the instructions outlined below to assemble the GENOSYL DS Injection Assembly as shown in Figure 21.

ILLUSTRATION

ACTION

1. Connectthe Inline Breathing Circuit Filter to the Gas Injection Adapter (22 mm ID × 22 mm OD).

1. Connectthe Adaptive Sensor to the inlet end of Gas Injection Adapter (22mm ID × 22 MM OD).

3.4.2 GENOSYL DS Mixer Assembly with Adaptive Sensor

If required, follow the instructions outlined below to assemble the GENOSYL DS Mixer Assembly with Adaptive Sensor as shown in Figure 22.

ILLUSTRATION

ACTION

1. Connectthe Inline Breathing Circuit Filter to the Adapter 22 mm ID × 22 mm ID.

1. Connectthe Adapter 22mm ID × 22 mm ID to the distal end of the Mixer.

1. Connectthe Gas Injection Adapter to the proximal end of the Mixer.

1. Connectthe Adaptive Sensor to the proximal end of the Gas Injection Adaptor

3.5 GENOSYL DS Console Connections

3.5.1 GENOSYL DS Gas Line Connections

Follow the steps listed below to connect the GENOSYL DS Gas Lines to both Consoles.

ILLUSTRATION | ACTION | Warnings, Cautions and Notes
 | 1. Pushand twistclockwise the short Y-end of the NO Injection Line (red) to the "NO" port (red)on the front panel of the Dosing Console.
 | 1. Pushand twistthe short Y-end of the Sample Line (blue) to the Gas Sample Port (blue)on the front of the Water Trap, attached to the Dosing Console. | NOTE
 | 1. Pushand twistthe short Y-end of the Sample Line (blue) to the Gas Sample Port (blue)on the front of the Water Trap, attached to the Dosing Console. | Ensure the Sample Lines are connected to the Water Traps on both Consoles.
 | 1. Push and twist clockwise the end of the Manual Ventilation Line (clear) to the Manual Ventilation Port (clear)on the front panel of the Dosing Console 2. Repeatsteps 1, 2, and 3 on the Back-up Console.

3.5.2 GENOSYL DS Sample Line Extension Connection

For use in the MR Environment, where a longer sample line is required follow the steps listed below to connect a Sample Line Extension. It is recommended to install the Sample Line Extension prior to initiation of dose.

ILLUSTRATION

ACTION

Warnings, Cautions and Notes

1. If actively dosing, switchto Manual Dosing Mode prior to completing the following steps (see Section 5.4for details on Manual Dosing Mode).

WARNING

Failure to switch to Manual Dosing Mode prior to installing a Sample Line Extension when the System is actively dosing may result in a spike in the NO dose delivered to the patient.

1. Turnthe blue Stopcock Valve, attached at the Gas Sample Tee, to the closed position as shown.

1. Pushand twistcounterclockwise the Luer-Lock Collar of the Sample Line to remove from the blue Stopcock Valve at the Gas Sample Tee.

1. Pushand twistclockwise the Luer-Lock Collar of the Sample Line onto the Sample Line Extension female connection.
2. Pushand twistclockwise the Luer-Lock Collar of the Sample Line onto the blue Stopcock Valve at the Gas Sample Tee.

1. PerformWater Trap / Sample Line Leak Test, as detailed in Section 2.13.

1. If actively dosing, switchback to Primary Dosing Mode (see Section 5.4.2for details on resuming Primary dosing).

3.5.3 Sample Line Filter Connection

In cases when additional filtration of the sample line may be required (e.g.: Aerosol Delivery), follow the steps listed below to connect a Sample Line Filter.

ILLUSTRATION

ACTION

Warnings, Cautions and Notes

1. Closethe blue stopcock to the position as shown

1. Disconnectthe blue sample line from the blue stopcock, keeping the blue stopcock connected to the patient circuit.

1. Pushand twistcounterclockwise the Luer-Lock Collar of the Sample Line to remove from the blue Stopcock Valve at the Gas Sample Tee.

1. Pushandtwistclockwise the male Luer-Lock Collar of the Sample Line Filter to the blue stopcock.

1. Openthe blue stopcock valve to the position as shown.

1. PerformWater Trap / Sample Line Leak test, as detailed in Section 2.13.

3.5.4 GENOSYL DS Adaptive Sensor Cable Connection

Follow the step below to connect the Adaptive Sensor Cable to the Dosing Console.

ILLUSTRATION | ACTION | Warnings, Cautions and Notes
 | 1. Connectthe Adaptive Sensor Cable to the Adaptive Sensor Port on front of the Dosing Console. | NOTE
 | 1. Connectthe Adaptive Sensor Cable to the Adaptive Sensor Port on front of the Dosing Console. | The Adaptive Sensor should only be connected to the Dosing Console.

3.5.5 GENOSYL DS Respiratory Circuit Connections

Follow the steps listed below to connect the Gas Lines to the Injection Assembly, Sample Tee, and Adaptive Sensor. If a Sample Tee already exists within the ventilator circuit, the Sample Line may be connected directly to the existing Sample Tee.

ILLUSTRATION | ACTION | Warnings, Cautions and Notes
 | 1. Pushand twistclockwise the Luer-Lock Collar from the NO Injection Line onto the Injection Assembly. | NOTE
 | 1. Pushand twistclockwise the Luer-Lock Collar from the NO Injection Line onto the Injection Assembly. | After connecting, the valve assembly may have rotated such that the orientation may appear different from what is shown here and on the display screen.
 | 1. Pushand twistclockwise the Luer-Lock Collar of the Sample Line onto the Sampling Port of the Gas Sample Tee. | NOTE
 | 1. Pushand twistclockwise the Luer-Lock Collar of the Sample Line onto the Sampling Port of the Gas Sample Tee. | Skip this step if a Gas Sample Tee is already connected and in-line with the ventilator circuit.
 | 1. Ensurethe blue Stopcock Valve is in the open position as shown.
 | 1. Connectthe distal end of the Adaptive Sensor Cable to the Adaptive Sensor on the Injection Assembly

3.6 Manual Ventilation (Bag) Connection

Follow the steps listed below to connect the Manual Ventilation Line to a manual bagging system.

ILLUSTRATION

ACTION

1. Attachthe barbed end of the Manual Ventilation Bag NO Adapter into the oxygen tubing from the oxygen source.
2. Attachthe other end of the NO Adapter to the oxygen port on the side of the Manual Ventilation Bag.
3. Connectthe Manual Ventilation Line (clear) to the NO Injection Port of the Manual Ventilation Bag NO Adapter.
4. Placethe Manual Ventilation Assembly in a clean accessible place if needed for future use.

3.7 Mechanical Ventilator Circuit Connections

Follow the steps outlined in this section to connect the GENOSYL DS Ventilator Circuit Assembly to the Mechanical Ventilator Circuit.

WARNING

- ALWAYS ensure the trigger sensitivity of the ventilator is checked after connecting the GENOSYL DS to the breathing circuit or when the dose is changed. The GENOSYL DS injects and samples gas from the patient respiratory circuit which may affect the triggering sensitivity of the ventilator.
- ALWAYS ensure the patient disconnect and high–pressure alarms are used with the ventilator.

NOTE

All ventilator connections should be assembled and inspected prior to connecting to the mechanical ventilator circuit.

ILLUSTRATION | ACTION | Warnings, Cautions and Notes
 | 1. Disconnectthe Inspiratory Tubing from the humidifier and attach it to the proximal end of the Injection Assembly to the Adaptive Sensor. 2. Attachthe distal end of the Injection Assembly to the humidifier.
 | 1. Insertthe Sample Tee into the ventilator circuit at the proximal end of the temperature probe closest to the patient. | NOTE
 | 1. Insertthe Sample Tee into the ventilator circuit at the proximal end of the temperature probe closest to the patient. | If a Gas Sample Tee is already connected and in-line with the ventilator circuit, connect the blue Sample Line directly to the existing Gas Sample Tee.

3.8 Gas Sampling During Aerosol Delivery

Follow the steps below to sample gas during Aerosol Delivery.

CAUTION

Pneumatic Nebulizers will dilute the delivered nitric oxide dose.

NOTE

Replace filter after each treatment period. Change the filter if necessary due to Line Occlusion Alarm.

ILLUSTRATION | ACTION | Warnings, Cautions and Notes
 | 1. Place the medication nebulizer downstream of the Gas Sample Tee on the inspiratory limb. | NOTE
 | 1. Place the medication nebulizer downstream of the Gas Sample Tee on the inspiratory limb. | This placement avoids contamination of the sample system and prevents Line Occlusion Alarm from occurring.
 | 1. Insert and Connectthe Sample Line Filter between the Sample Line and Blue Stopcock. (Refer to Section 3.5.3for detailed instructions)

GENOSYL®DS

SECTION 4
SYSTEM START-UP

4. SYSTEM START UP

4.1 Console Start-Up

Follow the instructions in this section to turn on both the Dosing and Back-up Consoles.

ILLUSTRATION | ACTION | Warnings, Cautions and Notes
 | 1. Pushthe Circular Power Connectors into the back of the top and bottomConsoles. 2. Connectthe main power cord to a grounded 120 V electrical outlet. | CAUTION
 | 1. Pushthe Circular Power Connectors into the back of the top and bottomConsoles. 2. Connectthe main power cord to a grounded 120 V electrical outlet. | ONLY use the GENOSYL DS with the power cord supplied by the manufacturer. Use of a generic power cord may cause output voltage instability leading to a touch screen failure. ALWAYS ensure the power cord is firmly seated into the power supply and the wall outlet. A loose connection can result in damage to the device or faulty operation.
 | 1. Pressthe Black Rocker Power Switch, located on the back of eachConsole, to the right (ON position) to power on bothConsoles.
 | 1. Pressthe Silver Power Button, located at the top left corner on the front panel of eachConsole, to turn on the display screens on bothConsoles. The display screen will illuminate, and the Consoles will beep, indicating the power is on. | CAUTION
 | 1. Pressthe Silver Power Button, located at the top left corner on the front panel of eachConsole, to turn on the display screens on bothConsoles. The display screen will illuminate, and the Consoles will beep, indicating the power is on. | The System will conduct an internal self-test. If an alarm or failure message should occur, refer to Section 10to resolve the issue.
 | 1. Pressthe Silver Power Button, located at the top left corner on the front panel of eachConsole, to turn on the display screens on bothConsoles. The display screen will illuminate, and the Consoles will beep, indicating the power is on. | NOTE
 | 1. Pressthe Silver Power Button, located at the top left corner on the front panel of eachConsole, to turn on the display screens on bothConsoles. The display screen will illuminate, and the Consoles will beep, indicating the power is on. | If the display screen does not turn on, see Troubleshooting, Section 10.8.

4.2 Cassette Insertion & Water Trap / Sample Line Leak Test

The following steps should be taken on both Consoles. Initiating Console Start-Up and inserting a Cassette for the Back-up Console at this stage will prepare it to serve as a Back-up for the Dosing Console.

Upon the insertion of a Cassette, a test will be initiated on each Console to check and ensure the integrity of the Water Traps and Sample Line (see Section 2.13). This helps ensure the accuracy of NO being delivered to the ventilator circuit.

The Water Trap / Sample Line Leak Test is automatically initiated upon one or both of the following conditions: 1) Insertion and seating of the Cassette if the measured NO is less than 1.0 ppm and/or 2) Insertion and seating of the Water Trap.

ILLUSTRATION | ACTION | Warnings, Cautions and Notes
 | The following steps should be taken to insert the Cassettes into the Consoles. | WARNING
 | The following steps should be taken to insert the Cassettes into the Consoles. | ALWAYS follow Cassette inspection instructions prior to insertion. Not inspecting the Cassette prior to insertion may lead to using a faulty Cassette, resulting in injury.
 | The following steps should be taken to insert the Cassettes into the Consoles. | NOTE
 | The following steps should be taken to insert the Cassettes into the Consoles. | Upon turning on the Consoles, the Cassette Indicator will display "Replace"
 | 1. Confirmthe Cassettes are blue. | WARNING
 | 1. Confirmthe Cassettes are blue. | Only use the orange External Transport Cassettes identified by orange color and transport sticker for use in external transport outside of the hospital.
 | 1. Confirmthe Cassettes are blue. | NOTE
 | 1. Confirmthe Cassettes are blue. | See Section 8for information about using the GENOSYL DS for external patient transfer outside of the hospital.
 | 1. Confirmthe Cassette State Window on eachCassette is blue. | WARNING
 | 1. Confirmthe Cassette State Window on eachCassette is blue. | DO NOT use the Cassette if the window is not blue. A Cassette State Window that is any color other than blue may affect the Cassette's ability to provide the correct NO dosage to the patient, which may cause injury or death.
 | 1. Confirmthe Cassette State Window on eachCassette is blue. | NOTE
 | 1. Confirmthe Cassette State Window on eachCassette is blue. | Cassette is inserted front first. The Cassette State Window is not visible when properly inserted. If the Cassette State Window is not blue, see Troubleshooting, Section 9.8
 | 1. Openthe Cassette Access Doors and inserttwo Cassettes into the Dosing Console and at least one Cassette into the Back-up Console. Push until it clicks. | NOTE
 | 1. Openthe Cassette Access Doors and inserttwo Cassettes into the Dosing Console and at least one Cassette into the Back-up Console. Push until it clicks. | Make sure Consoles are turned on before inserting the Cassette. The Water Trap / Sample Line Leak Test is automatically initiated when the Cassette has been insertedand the measured NO is less than 1.0 ppm. After the first Cassette is fully inserted, the Operator will have 60 seconds to close the blue Stopcock Valveto perform the test (Step 4below). Gas lines will need to be connected to the Console in order to pass the Water Trap / Sample Line Leak Test.
 |  | NOTE
 |  | The Display Screen will temporarily indicate the Cassette has been detected, then automatically transition to the Water Trap / Sample Line Leak Test screen.
 | 1. Followthe onscreen instructions on both Consoles. | NOTE
 | 1. Followthe onscreen instructions on both Consoles. | The screen will indicate the Water Trap / Sample Line Leak Test has started and the progress bar will be red until the Stopcock Valve has been closed, upon which it will then turn green if there is no leak detected. Pressing "Cancel Leak Test", will allow for dosing in Manual Dosing Mode. See Section 5.4for detail around dosing in Manual Dosing Mode.
 | 1. Followthe onscreen instructions on both Consoles. | CAUTION
 | 1. Followthe onscreen instructions on both Consoles. | Open the blue Stopcock Valve priorto pressing "Accept". Failure to do so will result in a line occlusion alarm.

4.2.1 Water Trap / Sample Line Leak Test Troubleshooting

NOTE

If the Water Trap / Sample Line Leak Test fails, follow the onscreen instructions below to resolve the issue. Also see Troubleshooting, Section 10.8.

ILLUSTRATION | ACTION | Warnings, Cautions and Notes
 | 1. If this screen is displayed, followthe onscreen instructions on both Consoles.
 | 1. Press"Confirm" on bothConsoles to begin a new Water Trap / Sample Line Leak Test. | NOTE
 | 1. Press"Confirm" on bothConsoles to begin a new Water Trap / Sample Line Leak Test. | NO Injection is held at 20 ppm until the completion of a successful Water Trap / Sample Line Leak Test.

GENOSYL®DS

SECTION 5
NITRIC OXIDE ADMINISTRATION

5. NITRIC OXIDE ADMINISTRATION

5.1 Nitric Oxide Dose Set-Up and Administration

The following steps are a continuation of Section 4.2, in which the Cassette will now be activated for nitric oxide administration.

WARNING

- MAKE SURE the System stabilizes to the prescribed concentration (ppm) of NO prior to leaving the Console unattended. Failure to do so could result in under delivery of the target NO, leading to injury or harm.
- ALWAYS constantly monitor the patient. System malfunctions can occur if device and patient are not monitored and can result in injury or death. Careful monitoring is required by care personnel whenever the System is used on a patient. The use of an alarm and a monitoring system does not give an absolute assurance of warning for every malfunction that may occur. Certain alarms may require immediate response.
- If the gas flow of the patient's respiratory device/ventilator should be interrupted or discontinued, the NO dose should be maintained by switching to Manual Dosing Mode or the target NO dose should be set to zero.

5.1.1 Setting a Dose when using a Circuit withan Adaptive Sensor

This section describes how to set a nitric oxide dose when an Adaptive Sensor is used in the patient circuit. Refer to Section 3.2for recommended set up diagrams.

ILLUSTRATION | ACTION | Warnings, Cautions and Notes
 | 1. Pressthe gray "Set" button on the display screen. | Note
 | 1. Pressthe gray "Set" button on the display screen. | The Adaptive Sensor must detect flow through the breathing circuit to set a dose.
 | 1. Enterthe prescribed dose in ppm on the electronic keypad. 2. PressOK to confirm the entry. | NOTE
 | 1. Enterthe prescribed dose in ppm on the electronic keypad. 2. PressOK to confirm the entry. | The time to reach target dose may vary up to 10 minutes.
 | 1. Enterthe prescribed dose in ppm on the electronic keypad. 2. PressOK to confirm the entry. | If unable to set the dose in Primary Dosing Mode, see Troubleshooting, Section 10.8.
 |  | NOTE
 |  | If manual ventilation is required, proceed to Section 5.4. When adjusting dose, proceed to Section 5.2. If dosing is completed, proceed to Section 6.1.
 |  | NOTE
 |  | The display screen will look as shown after completing steps 1-3.
 |  | NOTE
 |  | The NO2sensor reading may appear as "—" for the first 30 seconds of dosing while the sample System is preparing.

5.1.2 Setting a Dose when using a Circuit withoutan Adaptive Sensor

This section describes how to set a nitric oxide dose when an Adaptive Sensor is not used in the patient circuit, such as when initiating a dose when using a Console as Backup (Section 5.5). Refer to Section 3.2for recommended set up diagrams. In the absence of an Adaptive Sensor, the GENOSYL DS will properly deliver and control nitric oxide dose. However, the user will have to manually select a Total Flow range.

ILLUSTRATION

ACTION

Warnings, Cautions and Notes

1. Pressthe gray "Set" button on the display screen.

1. ConfirmTotal Flow range is appropriately selected.
2. Enterthe prescribed dose in ppm on the electronic keypad.
3. PressOK to confirm the entry.

NOTE

The time to reach target dose may vary up to 10 minutes.
If unable to set the dose in Primary Dosing Mode, see Troubleshooting, Section 10.8.

NOTE

If manual ventilation is required, proceed to Section 5.4.
When adjusting dose, proceed to Section 5.2.
If dosing is completed, proceed to Section 6.1.

NOTE

The display screen will look as shown after completing steps 1-3.

NOTE

The NO2sensor reading may appear as "--" for the first 30 seconds of dosing while the sample system is preparing.

5.2 Adjusting the Dose

To adjust the dose of nitric oxide administered per hospital protocol or physician order, follow the instructions listed below.

5.2.1 Adjusting the Dose when using a Circuitwithan Adaptive Sensor

ILLUSTRATION | ACTION | Warnings, Cautions and Notes
 | 1. Pressthe gray "Set" button to access the electronic keypad on the display screen on the Dosing Console.
 | 1. Enterthe prescribed dose using the electronic keypad. 2. Press"OK" to confirm the dose and to start dosing administration. | NOTE
 | 1. Enterthe prescribed dose using the electronic keypad. 2. Press"OK" to confirm the dose and to start dosing administration. | If dosing is complete, proceed to Section 6.

5.2.2 Adjust the Dose and Flow Range when using a Circuitwithoutan Adaptive Sensor

ILLUSTRATION | ACTION | Warnings, Cautions and Notes
 | 1. Pressthe gray "Set" button to access the electronic keypad on the display screen on the Dosing Console.
 | 1. Enterthe prescribed ppm dose using the numeric keypad. 2. Adjust Total Flow range, if necessary. 3. Press"OK" to confirm the dose and to start dosing administration. | NOTE
 | 1. Enterthe prescribed ppm dose using the numeric keypad. 2. Adjust Total Flow range, if necessary. 3. Press"OK" to confirm the dose and to start dosing administration. | If dosing is complete, proceed to Section 6.

5.3 Replacement of a Depleted Cassette

The GENOSYL DS automatically switches from the dosing Cassette to the secondary Cassette in the Dosing Console once the Cassette is depleted if a secondary Cassette is properly inserted and preheated. After transition, the depleted Cassette is automatically ejected.

CAUTION

User should always have a secondary Cassette inserted in the Dosing Console and preheated in order for auto transition to occur. User should replace depleted Cassette as soon as possible after ejection.

ILLUSTRATION

ACTION

Warnings, Cautions and Notes

NOTE

The Console will automatically transition to the secondary Cassette if properly inserted and preheated. The screen to the left will be displayed during the transition process.

1. Follow onscreen instructions to replace Cassette.

5.4 Manual Mode

NOTE

- When entering Manual Dosing Mode, the set target dose in Primary Dosing Mode will carry over to Manual Dosing Mode if 5 ppm or greater. Less than 5 ppm set target dose in Primary Dosing Mode will default to 5 ppm dose in Manual Dosing Mode. However, dose and flow rate may need to be adjusted for specific situations. The GENOSYL DS Smart Feedback System™ is disabled while in Manual Dosing Mode. To reinitiate the Smart Feedback System, switch back to Primary Dosing Mode as soon as the situation permits.
- After a Console is in Manual Dosing Mode for more than two minutes, a reminder tone will sound in ten second intervals to alert the user that the Console is still in Manual Dosing Mode.

5.4.1 Manual Ventilation Use (Bagging)

This section will describe NO administration when manual ventilation is required.

WARNING

- ALWAYS ensure that the manual flow displayed on the Console matches the flow set into the resuscitation bag. Incorrect flow settings may result in an incorrect estimation of NO delivery. If the flow into the manual equipment is too low, there is risk of overdosing the patient with NO.
- ALWAYS squeeze the bag several times, after starting fresh gas flow, to empty residual gas in the bag prior to using the System to ventilate a patient. Failure to do so could result in higher NO2levels being delivered to the patient.
- ALWAYS use the smallest bag adequate to deliver the desired tidal volume. Failure to do so could result in higher NO2levels being delivered to the patient.
- ONLY use a manual resuscitation bag with the GENOSYL DS for a short time (e.g., less than one hour) when on battery only. Otherwise, the System may shut off and may result in injury or death.

ILLUSTRATION | ACTION | Warnings, Cautions and Notes
 | 1. Ensurethe oxygen flow source is set appropriately or adjust as needed. 2. Pressthe button "Switch to Manual" on the Dosing Console.
 | 1. Press "Confirm" to switch to Manual Dosing. | WARNING
 | 1. Press "Confirm" to switch to Manual Dosing. | If the dilution flow rate displayed on the screen does not match the wall source, then the estimated NO may be inaccurate.
 |  | NOTE
 |  | Dosing has been initiated at the same dose (ppm) as set in Primary Dosing Mode. If the primary dosing was set at "0" prior to pressing the "Switch to Manual" button, the estimated NO will also be at "0" and will need to be adjusted. If the dose was set between 1 and 5 ppm prior to pressing the "Switch to Manual" button, the estimated NO dose will also be at"5 ppm" and may be adjusted. In the event dose is initiated in Manual Dosing Mode, the console will default to 20 ppm, which can be adjusted as needed.
 | 1. To resumeprimary dosing, see Section 5.4.3. | NOTE
 | 1. To resumeprimary dosing, see Section 5.4.3. | If an adjustment of the NO concentration is required, press the green up and down arrows. If an adjustment to the Dilution Flow Rate is required while in Manual Dosing Mode, press the LPM value and a dropdown menu will expand. Press the prescribed value. The new value will be highlighted in blue and the dropdown menu will collapse.

5.4.2 Preset Manual Dosing Mode Flow Rate (OPTIONAL)

User has the option to preset a Manual Dosing Mode Flow rate. This can be completed during set up or at any time.

ILLUSTRATION | ACTION | Warnings, Cautions and Notes
 | 1. Navigate to the "Settings" Tab.
 | 1. Selectthe Flow Rate from the drop-down menu. | NOTE
 | 1. Selectthe Flow Rate from the drop-down menu. | The Console will default to a Flow Rate of 10 LPM if not adjusted. Any adjustment will be retained until the Console is powered down.

5.4.3 Resuming Primary Dosing

This section describes the process for resuming primary dosing from Manual Mode.

ILLUSTRATION | ACTION | Warnings, Cautions and Notes
 | 1. Pressthe "Switch to Primary" button at the top of the Manual Mode screen.
 | 1. Press"Confirm" to start dosing or "Cancel" to cancel. | NOTE
 | 1. Press"Confirm" to start dosing or "Cancel" to cancel. | The NO dose used in Manual Mode will become the set target dose in Primary Mode.
 |  | NOTE
 |  | The display screen will look as shown after completing steps 1-2.

5.5 Console Use as a Back-up

This section describes the process of activating the Cassette in the Back-up Console. Delivery of NO will begin immediately upon Cassette activation.

DISPLAY | ACTION | Warnings, Cautions and Notes
 | 1. Press the "Set" button on the Back-up Console which will display the NO dose electronic keypad and Flow Selection menu.
 | 1. Confirm Dose and Total Flow range is appropriately selected. 2. Press "OK" to confirm entry | NOTE
 | 1. Confirm Dose and Total Flow range is appropriately selected. 2. Press "OK" to confirm entry | The Back-up Console screen will be as shown. The default Total Flow range displayed will be <2.5LPM and the default dose will be 20 ppm unless otherwise selected by the user. See Section 5.1.2 The Back-up Console is now the Dosing Console.
 | 1. Connect the Adaptive Sensor Cable to the front of the new Dosing Console.

GENOSYL®DS

SECTION 6
CONSOLE SHUTDOWN

6. CONSOLE SHUTDOWN AND CASSETTE DISPOSAL

WARNING

NEVER turn the rear power switch OFF until the System has gone through a controlled shutdown or instructed by VERO Technical Support. Turning the rear power switch OFF prematurely (e.g., while it is still in use) will immediately shut down the device. This may result in interruption in NO delivery to the patient, which may cause injury or death.

CAUTION

NEVER turn the rear power switch OFF until the System has gone through a controlled shutdown or instructed by VERO Technical Support. Turning the rear power switch OFF prematurely (e.g., while it is still in use) will immediately shut down the device and may cause improper operation upon restart.

NOTE

It is recommended that the Console be rebooted at least once every 30 days.

6.1 Console Shutdown

If the administration of NO must be stopped, then the dose level must be set to "0". The following procedure describes how to remove the Cassette and the following section will describe how to shut down the Console.

DISPLAY | ACTION | Warnings, Cautions and Notes
 | 1. Pressthe gray "Set" button to access the electronic keypad on the display screen.
 | 1. Setthe dose to "0" using the electronic keypad. 2. Press"OK" to confirm the entry.
 | 1. If the "Settings" tab is not displayed, pressthe "Menu" tab to access the sub-level tabs. 2. Pressthe "Settings" tab on the display menu. 3. Pressthe red "System Shutdown" icon.
 | 1. Reviewon screen prompt. 2. Press"Confirm" to confirm shutdown. 3. Waituntil the Console shuts down, the display screen appears blank, and the Console emits an audible beep. | NOTE
 | 1. Reviewon screen prompt. 2. Press"Confirm" to confirm shutdown. 3. Waituntil the Console shuts down, the display screen appears blank, and the Console emits an audible beep. | If the System does not shut down, see Troubleshooting , Section 10.8. The screen will inform user if Cassette should be saved or disposed of. Refer to Section 2.14Shutdown Cassette Status Indicator description.
 | 1. Openthe Cassette Access Door.
 | 1. Removethe Cassettes by pulling the Cassette straight out. 2. Disposethe inerted Cassettes per hospital policy. | NOTE
 | 1. Removethe Cassettes by pulling the Cassette straight out. 2. Disposethe inerted Cassettes per hospital policy. | The Console will inert any remain contents from a dosing Cassette upon ejection, rendering it unusable. If a Cassette has only been preheated, and not used for dosing, the contents have not been inerted and it can still be used. The Cassette State Window will remain blue on Cassettes that have not been inerted.
 | 1. Pressthe Black Rocker Power Switch to the "OFF" position. 2. Repeatsteps 1-13 for the other Console. | WARNING
 | 1. Pressthe Black Rocker Power Switch to the "OFF" position. 2. Repeatsteps 1-13 for the other Console. | NEVER turn the rear power switch OFF until the System has gone through a controlled shutdown or instructed by VERO Technical Support. Turning the rear power switch OFF prematurely (e.g., while it is still in use) will immediately shut down the device. This may result in interruption in NO delivery to the patient, which may cause injury or death.
 | 1. Pressthe Black Rocker Power Switch to the "OFF" position. 2. Repeatsteps 1-13 for the other Console. | CAUTION
 | 1. Pressthe Black Rocker Power Switch to the "OFF" position. 2. Repeatsteps 1-13 for the other Console. | NEVER turn the rear power switch OFF until the System has gone through a controlled shutdown or instructed by VERO Technical Support. Turning the rear power switch OFF prematurely (e.g., while it is still in use) will immediately shut down the device and may cause improper operation upon restart.

6.2 Cassette Disposal

Following dosing use, any remaining Cassette liquid contents in a dosing Cassette are purged into an inerting chamber that is built into the Cassette, where the contents are chemically neutralized, rendering the Cassette safe for disposal. When the Cassette liquid contents are emptied into the inerting chamber, the Cassette State Window on the front of the Cassette reddens and bleaches from its original blue color, indicating the Cassette is depleted. The Cassette can now be disposed of per hospital policy.

GENOSYL®DS

SECTION 7
USING THE SYSTEM IN THE MR SCANNER ROOM

7. USING THE SYSTEM IN THE MR SCANNER ROOM

WARNING

- The GENOSYL DS is classified as MR Conditional with MR scanners of 1.5 or 3.0 Tesla strength ONLY in areas where the field strength is less than 100 gauss.
- ALWAYS operate at a fringe field of less than 100 gauss. This device contains ferromagnetic components and may experience strong attraction close to the magnet.
- DO NOT exceed 100 gauss; System operation may be impacted. Confirm Cart caster lock function. Optionally connect tether.
- NEVER use the GENOSYL DS in the MR scanner room without gauss alarms installed.
- ALWAYS verify at least one gauss alarm is functioning properly prior to use in the MR environment.
- DO NOT use the GENOSYL DS in the MR environment if neither gauss alarm is functional.
- ALWAYS move System away from the MR scanner if the gauss alarm sounds. The gauss alarm will sound if the System is too close to the MR scanner. Move System away from the MR scanner until the gauss alarm stops sounding.
- ALWAYS verify that the GENOSYL DS Cart casters are locked after positioning the System in the MR scanner room.
- ALWAYS verify that the GENOSYL DS is securely attached to the Cart.
- ALWAYS arrange power cord, MR patient gas sample line, and NO delivery line to avoid entanglement, strangulation and/or a trip hazard.
- DO NOT use the GENOSYL DS in the MR environment if the Cart moves when the brake caster locks are engaged.
- NEVER perform NO or NO2calibration within the MR scanner room. Calibration equipment is a potential projectile hazard.

NOTE

Refer to Section 13.11for MR Signal-to-Noise Ratio and Artifact Dimension Analysis

7.1 Connection to the Ventilator Breathing Circuit

To connect the GENOSYL DS to an MR Conditional ventilator, see Section 3.2for example breathing circuits. When using the GENOSYL DS in the MR environment, a Sample Line Extension may be required. See Section 3.5.2for steps to install the Sample Line Extension.

NOTE

- Connections to various ventilators are unique to each manufacturer as well as their corresponding disposable circuits.
- A Sample Line Extension may be required. Refer to Section 3.5.2for instructions to install a Sample Line Extension.

7.2 Transferring to and from the MR Scanner Room

WARNING

- NEVER use the GENOSYL DS in the MR scanner room without gauss alarms installed.
- DO NOT use the GENOSYL DS in the MR environment if neither gauss alarm is functional.
- ALWAYS verify at least one gauss alarm is functioning properly prior to use in the MR environment.
- ALWAYS verify that the GENOSYL DS is securely attached to the Cart.
- NEVER perform NO or NO2calibration within the MR scanner room. Calibration equipment is a potential projectile hazard.

1. Verifythat both gauss alarms are installed on the GENOSYL DS Cart.

2. Movethe patient, MR conditional ventilator circuit, and GENOSYL DS into the MR scanner room.

3. Positionthe GENOSYL DS outside of the MR exclusion zone, as shown in Figure 23.

WARNING

ALWAYS move System away from the MR scanner if the gauss alarm sounds. The gauss alarm will sound if the System is too close to the MR scanner. Move System away from the MR scanner until the gauss alarm stops sounding.

4. Engagethe locks on wheels and confirm caster lock function. Attaching a facility supplied tether to the System Cart handle may be utilized as a redundant means to limit the distance the Cart can move.

WARNING

- ALWAYS verify that the GENOSYL DS Cart casters are locked after positioning the System in the MR scanner room.
- DO NOT use the GENOSYL DS in the MR environment if the Cart moves when the brake caster locks are engaged.

5. Movethe patient, MR conditional ventilator, and GENOSYL DS outside of the MR scanner room.

6. Verifyventilator and GENOSYL DS function following transition from the MR scanner room.

GENOSYL®DS

SECTION 8
EXTERNAL TRANSPORT

8. EXTERNAL TRANSPORT

WARNING

- ALWAYS use the GENOSYL DS in accordance with the indications, usage, contraindications, warnings, and precautions described in the GENOSYL prescribing information and labeling. Refer to latest approved prescribing information and labeling prior to use.
- The approved patient population for the GENOSYL DS as specified in the drug labeling for GENOSYL (nitric oxide) for inhalation, is limited to neonates. The GENOSYL DS is not intended to be used in other patient populations.
- ALWAYS ensure the GENOSYL DS Dosing and Back-up Consoles are securely affixed to the External Transport Mounts when the System used in a transport vehicle.
- ALWAYS ensure Consoles are placed into External Transport Mode before inserting a Cassette for external transport outside of the hospital.
- ALWAYS have a second Console present and properly connected when a Dosing Console is connected to the patient. If the Dosing Console malfunctions, switch to the Back-up Console. If the Back-up Console is not available or properly connected, this may result in patient injury or death.
- ONLY use External Transport Cassettes, identified by orange color and transport sticker, in external transport outside of the hospital.
- ALWAYS ensure the External Transport Mounts are secured during patient transport, per hospital protocols.

CAUTION

Prolonged use in dry environments without humidification will damage the gas sensors. Supplemental humidification providing greater than 20% relative humidity (RH) in the patient circuit is recommended.

Compatibility testing has demonstrated performance meeting requirements for the GENOSYL DS operating range of 0 to 80 ppm with the following external transport ventilation devices at the operating ranges shown in Table 3, including Manual Ventilation mode, while External Transport Mode is turned ON and while using an External Transport Cassette.

- Hamilton T1
- International Bio-Med Crossvent 2+
- International Bio-Med MVP-10

WARNING

- The GENOSYL DS injects and samples gas from the patient respiratory circuit which may affect the triggering sensitivity of the ventilator. ALWAYS ensure the trigger sensitivity of the ventilator is checked after connecting the GENOSYL DS to the breathing circuit or when the dose is changed, and adjust trigger sensitivity as necessary. Failure to do so may lead to ventilator auto cycling or apnea alarm.
- ALWAYS ensure the patient disconnect and high–pressure alarms are used with the ventilator.
- ONLY use the GENOSYL DS with Bio-Med Crossvent 2+ with Constant Flow ON. Not doing so may lead to elevated NO2levels or dose variability.

CAUTION

- When using spontaneousbreathing modes on respiratory device, NO2levels may exceed 3.0 ppm when dosing ≥ 57 ppm NO into 100% FiO2and maximum bias flow resulting in nitric oxide delivery interruption. Once sample value of NO2is below 3.0 ppm, the Console will auto resume delivery of NO at set dose. Refer to Section 12.1.5 Table 13for additional information.
- When using non-spontaneousbreathing modes on respiratory device, NO2levels may exceed 3.0 ppm when dosing ≥ 63 ppm NO or greater into 100% FiO2and maximum bias flow resulting in nitric oxide delivery interruption. Once sample value of NO2is below 3.0 ppm, the Console will auto resume delivery of NO at set dose. Refer to Section 12.1.5 Table 13for additional information.

Table 3: External Transport Ventilation Devices Compatibility Testing Ranges
Setting | Range | Unit
Inspiratory Flow Rate | 2-120 | LPM
Respiratory Rate | 6-60 | BPM
Peak Inspiratory Pressure | 0-70 | cmH2O
Positive End Expiratory Pressure | 0-20 | cmH2O

For use in patient external transport, the Dosing and Back-up Consoles must be securely mounted within the transport vehicle per hospital transport protocols. Figure 25illustrates the GENOSYL DS in an External Transport Mount.

Prior to using the GENOSYL DS in external transport, both Consoles must have External Transport Mode ON with two External Transport Cassettes in the Dosing Console and at least one External Transport Cassette inserted into the Back-up Console. See Figure 26for a diagram of the External Transport Cassette and Section 8.2.1for instructions to turning External Transport Mode ON.

External Transport Cassette in packaging

Unused External Transport Cassette

Inerted External Transport Cassette

Figure 26: External Transport Cassette

Example circuit diagrams for connection of the GENOSYL DS to a transport ventilator are shown in Figure 27(International Bio-Med Circuit) and Figures 28and 29for other conventional ventilators.

Additional disposable items recommended for external transport may include:

- GENOSYL External Transport Cassettes
- GENOSYL DS Gas Lines
- Water Trap
- GENOSYL DS Manual Bag NO Adapter
- Components for connection to breathing circuit

External transport equipment weight should be calculated to ensure transport system meets weight allowance.

Table 4: External Transport Equipment Specifications
Part Description | Weight per Unit | Dimensions | Number Required | Total Weight
Console | 8.85 kg (19.75 lb) | 40.6 cm × 34.29 cm × 17 cm (16 in × 13.5 in × 6.75 in) | 2 | 17.7 kg (39.5 lb)
External Transport Cassette | 0.42 kg (0.93 lb) | 11.4 cm × 3.8 cm × 13 cm (4.5 in × 1.5 in × 5.1in) | 3 | 1.26 kg (2.79 lb)
External Transport Mount | 2.22 kg (4.89lb) | 40.64 cm × 32.77 cm × 8.89 cm (16 in × 12.9 in × 3.5 in) | 2 | 4.44 kg (9.78 lb)
Quick Connect Plate | 1.52 kg (3.35 lb) | 46.36 cm × 27.18 cm × 0.64 cm (18.25 in × 10.70 in × 0.25 in) | (1 Optional) | 1.52 kg (3.35 lb)
Power Supply | 2.07 kg (4.56 lb) | 14.6 ft | 1 | 2.07 kg (4.56 lb)

Note: All sizes and weights are approximate and may vary slightly.

8.1 External Transport Set-Up and Ventilator Circuit Schematics

8.1.1 Securing a Console in a Transport Mount

GENOSYL DS Consoles must be secured into the External Transport Mount before used in external transport.

ILLUSTRATION | ACTION | WARNINGS, CAUTIONS, AND NOTES
 | 1. Confirman External Transport Mount is secured to the external transport sled. 2. Placethe Console into the External Transport Mount. | WARNING
 | 1. Confirman External Transport Mount is secured to the external transport sled. 2. Placethe Console into the External Transport Mount. | ALWAYS ensure the External Transport Mounts are secured during patient transport, per hospital protocols. ALWAYS ensure the GENOSYL DS Dosing and Back-up Consoles are securely affixed to the External Transport Mounts when the System will be used in an external transport vehicle.
 | 1. Pullthe strap on top of the Console securely tight to cinch into place. 2. Repeatsteps 1-3 for the other Console.

NOTE

Connections to various ventilators as well as their corresponding disposable circuits are unique to each manufacturer.

8.1.2 Connection to an International Bio-Med External Transport Ventilator Circuit

An example circuit diagram for connection of the GENOSYL DS to a dual-limb external transport ventilator is shown in Figure 27.The dual-limb circuit is used for ventilators such as the International Bio-Med Crossvent 2+ and International Bio-Med MVP-10.

Follow the steps outlined below to connect the GENOSYL DS to a Dual-Limb External Transport Ventilator Circuit for ventilators such as the International Bio-Med Crossvent 2+ and International Bio-Med MVP-10.

ILLUSTRATION

ACTION

1. Obtainone (1) Sample Tee, 3/8" Barbed, one (1) GENOSYL DS Adaptive Sensor, one (1) NO Gas Injection Adapter, and one (1) Injection Line Filter.

1. Connectthe GENOSYL DS Adaptive Sensor, NO Gas Injection Adapter, and the Injection Line Filter to create the Gas Injection Assembly.

1. Connectthe GENOSYL DS Adaptive Sensor of the Gas Injection Assembly with Injection Line Filter to the ventilator outlet port.

1. Connectthe inspiratory limb inlet to the NO Gas Injection Adapter of the Gas Injection Assembly with Injection Line Filter.

1. Locate and cutthe noncorrugated tubing at the center of the smooth segment closest to the patient wye.

1. Insertthe barbed ends of the Sample Tee, 3/8" Barbed into both ends of the cut tubing.

1. Pushand twistclockwise the Luer-Lock Collar from the NO Injection Line onto the Injection Assembly with Injection Line Filter.
2. Pushand twistclockwise the Luer-Lock Collar of the Sample Line Stopcock onto the Sampling Port of the Sample Tee, 3/8" Barbed.

Instructions for connecting gas lines to GENOSYL DS Consoles can be found in Section 3.5.1. Section 3.5.4covers connecting an Adaptive Sensor Cable to Dosing Console, and Section 3.5.5details connecting it to the Adaptive Sensor on the Injection Assembly.

8.1.3 Connection to a Conventional External Transport Ventilator

An example circuit diagram for connection of the GENOSYL DS to an external transport ventilator when using an Injection Assembly with Adaptive Sensor is shown in Figure 28and when using a Mixer Assembly with Adaptive Sensor is shown in Figure 29with transport ventilators such as the Hamilton T1. See Section 12.2 Table 15for applicable use scenarios.

8.1.3.1 Connection to a Conventional External Transport Ventilator using an Injection Assembly with Adaptive Sensor

Follow the instructions outlined below to assemble the GENOSYL DS Injection Assembly with Adaptive Sensor.

ILLUSTRATION

ACTION

1. Obtainone (1) Gas Sample Tee, one (1) GENOSYL DS Adaptive Sensor, one (1) NO Gas Injection Adapter, and one (1) Injection Line Filter.

1. ConnectGENOSYL DS Adaptive Sensor, NO Gas Injection Adapter, and the Injection Line Filter to create the Gas Injection Assembly.

1. Connectthe GENOSYL DS Adaptive Sensor of the Gas Injection Assembly with Injection Line Filter to the ventilator outlet port.

1. Connectthe inspiratory limb inlet to the NO Gas Injection Adapter of the Gas Injection Assembly with Injection Line Filter.

1. Insertthe Sample Tee into the ventilator circuit at the proximal end of the temperature probe closest to the patient.

1. Pushand twistclockwise the Luer-Lock Collar from the NO Injection Line onto the Injection Assembly with Injection Line Filter.
2. Pushand twistclockwise the Luer-Lock Collar of the Sample Line Stopcock onto the Sampling Port of the Sample Tee, 3/8" Barbed.

Instructions for connecting gas lines to GENOSYL DS Consoles can be found in Section 3.5.1. Section 3.5.4covers connecting an Adaptive Sensor Cable to Dosing Console, and Section 3.5.5details connecting it to the Adaptive Sensor on the Injection Assembly.

8.1.3.2 Transport Ventilator Circuit Set-Up and Connections using Mixer Assembly with Adaptive Sensor

Follow the instructions outlined below to assemble the GENOSYL DS Mixer Assembly with Adaptive Sensor.

ILLUSTRATION

ACTION

1. Obtainone (1) Inline Breathing Circuit Filter, (1) Mixer, (1) Adapter, (1) Adaptive Sensor (1), NO Gas Injection Adapter, and (1) Gas Sample Tee.

1. Connectthe GENOSYL DS Adaptive Sensor, NO Gas Injection Adapter, Mixer, Adapter and the Inline Breathing Circuit Filter to create the Mixer Assembly.

1. Connectthe GENOSYL DS Adaptive Sensor of the Mixer Assembly to the ventilator outlet port.

1. Connectthe inspiratory limb inlet to the NO Gas Injection Adapter of the Mixer Assembly with Adaptive Sensor.

1. Insertthe Sample Tee into the ventilator circuit at the proximal end of the temperature probe closest to the patient.

1. Pushand twistclockwise the Luer-Lock Collar from the NO Injection Line onto the Injection Assembly with Injection Line Filter.
2. Pushand twistclockwise the Luer-Lock Collar of the Sample Line Stopcock onto the Sampling Port of the Sample Tee, 3/8" Barbed.

Instructions for connecting gas lines to GENOSYL DS Consoles can be found in Section 3.5.1. Section 3.5.4covers connecting an Adaptive Sensor Cable to Dosing Console, and Section 3.5.5details connecting it to the Adaptive Sensor on the Injection Assembly.

8.2 Using the GENOSYL DS for External Transport

8.2.1 Switching External Transport Mode ON

Both the Dosing Console and the Back-up Console must have External Transport Mode ON before use in external transport.

ILLUSTRATION | ACTION | WARNINGS, CAUTIONS, AND NOTES
 | 1. Navigate to the "Settings" tab. | NOTE
 | 1. Navigate to the "Settings" tab. | Proceed to Section 8.2.2if External Transport Mode is already enabled.
 | 1. Pressthe "External Transport Mode OFF" button. | WARNING
 | 1. Pressthe "External Transport Mode OFF" button. | ALWAYS ensure Consoles are placed into External Transport Mode before inserting a Cassette for external transport outside of the hospital.
 | 1. Press"Confirm" to proceed.
 | 1. Enter the external transport PIN. 2. Press"OK" to confirm the entry. | NOTE
 | 1. Enter the external transport PIN. 2. Press"OK" to confirm the entry. | If you do not have the PIN, contact VERO Technical Support at 877.337.4118.
 | 1. Confirm External Transport Mode is ON.

8.2.2 Inserting an External Transport Cassette

The following steps should be taken on both Consoles. External Transport Cassettes must be used for external transport. While a Console has External Transport Mode turned ON, the Console will only allow External Transport Cassettes to preheat. If a Hospital Cassette is inserted, the Console will display an informational message and eject the Hospital Cassette (See Section 9.6).

Upon the insertion of a Cassette, a test will be initiated on the Console to check and ensure the integrity of the Water Traps and Sample Line (see Section 2.13), this helps ensure the accuracy of NO being delivered to the ventilator circuit.

ILLUSTRATION | ACTION | Warnings, Cautions and Notes
 | 1. Confirmboth Consoles have External Transport Mode ON. | WARNING
 | 1. Confirmboth Consoles have External Transport Mode ON. | ALWAYS follow Cassette inspection instructions prior to insertion. Not inspecting the Cassette prior to insertion may lead to using a faulty Cassette, resulting in injury. ALWAYS ensure Consoles are placed into External Transport Mode before inserting a Cassette for external transport outside of the hospital.
 | 1. Confirmboth Consoles have External Transport Mode ON. | NOTE
 | 1. Confirmboth Consoles have External Transport Mode ON. | Upon turning on the Consoles, the Cassette indicator will display "Replace"
 | 1. Confirmthe Cassettes are External Transport Cassettes. | WARNING
 | 1. Confirmthe Cassettes are External Transport Cassettes. | ONLY use External Transport Cassettes, identified by orange color and transport sticker, in external transport outside of the hospital.
 | 1. Confirmthe Cassette State Window on eachCassette is blue.
 | 1. Openthe Cassette Access Doors and inserttwo Cassettes into the Dosing Console and at least one Cassette into the Back-up Console. Push until it clicks. | NOTE
 | 1. Openthe Cassette Access Doors and inserttwo Cassettes into the Dosing Console and at least one Cassette into the Back-up Console. Push until it clicks. | Make sure Consoles are turned on before inserting the Cassette. The Water Trap / Sample Line Leak Test is automatically initiated when the Cassette has been insertedand the measured NO is less than 1.0 ppm. After the first Cassette is fully inserted, the Operator will have 60 seconds to close the blue Stopcock Valveto perform the test (Step 5below). Gas lines will need to be connected to the Console in order to pass the Water Trap / Sample Line Leak Test.
 |  | NOTE
 |  | The Display Screen will temporarily indicate the Cassette has been detected, then automatically transition to the Water Trap / Sample Line Leak Test screen.
 | 1. Followthe onscreen instructions on both Consoles. | WARNING
 | 1. Followthe onscreen instructions on both Consoles. | DO NOT use the Cassette if the window is not blue. A Cassette State Window that is any color other than blue may affect the Cassette's ability to provide the correct NO dosage to the patient, which may cause injury or death.
 | 1. Followthe onscreen instructions on both Consoles. | NOTE
 | 1. Followthe onscreen instructions on both Consoles. | The screen will indicate the Water Trap / Sample Line Leak Test has started and the progress bar will be red until the stopcock valve has been closed, upon which it will then turn green if there is no leak detected. Pressing "Cancel Leak Test", will allow for dosing in Manual Dosing Mode. See Section 8.2.6 Using Manual Dosing Modewhile External Transport Mode is Enabled for detail around dosing in Manual Dosing Mode. Cassette is inserted front first. The Cassette State Window is not visible when properly inserted. If the Cassette State Window is not blue, see 10.8 Troubleshooting
 | 1. Followthe onscreen instructions on both Consoles. | CAUTION
 | 1. Followthe onscreen instructions on both Consoles. | Open the blue Stopcock Valve priorto pressing "Accept". Failure to do so will result in a line occlusion alarm.
 | 1. Ensure the door latch is in the down position to keep the door closed.

8.2.3 Setting a Dose in External Transport Mode with an Adaptive Sensor

This section describes how to set a nitric oxide dose while External Transport Mode is ON, and an Adaptive Sensor is used in the patient circuit. Refer to Section 8.1.2 and 8.1.3for recommended set up diagrams.

ILLUSTRATION | ACTION | Warnings, Cautions and Notes
 | 1. Pressthe gray "Set" button on the display screen. | NOTE
 | 1. Pressthe gray "Set" button on the display screen. | The Adaptive Sensor must detect flow through the respiratory circuit to set a dose.
 | 1. Enterthe prescribed dose in ppm on the electronic keypad. 2. Press"OK" to confirm the entry. | NOTE
 | 1. Enterthe prescribed dose in ppm on the electronic keypad. 2. Press"OK" to confirm the entry. | The time to reach target dose may vary up to 10 minutes. If unable to set the dose in Primary Dosing Mode, see Troubleshooting, Section 10.8.
 |  | NOTE
 |  | If manual ventilation is required, proceed to Section 8.2.6. When adjusting dose, proceed to Section 8.2.5. If dosing is completed, proceed to Section 8.2.8.
 |  | NOTE
 |  | The display screen will look as shown after completing steps 1-3.
 |  | NOTE
 |  | The NO2sensor reading may appear as "—" for the first 30 seconds of dosing while the sample system is preparing.

8.2.4 Setting a Dose in External Transport Mode without an Adaptive Sensor

This section describes how to set a nitric oxide dose while External Transport Mode is ON without an Adaptive Sensor. In the absence of an Adaptive Sensor, the GENOSYL DS will properly deliver and control nitric oxide dose. However, the user will have to manually select a Total Flow range.

ILLUSTRATION

ACTION

Warnings, Cautions and Notes

1. Pressthe gray "Set" button on the display screen.

1. ConfirmTotal Flow range is appropriately selected.
2. Enterthe prescribed dose in ppm on the electronic keypad.
3. Press"OK" to confirm the entry.

NOTE

The time to reach target dose may vary up to 10 minutes.
If unable to set the dose in Primary Dosing Mode, see Troubleshooting, Section 10.8.

NOTE

If manual ventilation is required, proceed to Section 8.2.6.When adjusting dose, proceed to Section 8.2.5.
If dosing is completed, proceed to Section 8.2.8.

NOTE

The display screen will look as shown after completing steps 1-4.

NOTE

The NO2sensor reading may appear as "--" for the first 30 seconds of dosing while the sample system is preparing.

8.2.5 Adjusting a Dose in External Transport Mode

ILLUSTRATION | ACTION | Warnings, Cautions and Notes
 | 1. Pressthe gray "Set" button to access the electronic keypad on the display screen on the Dosing Console.
 | 1. Enterthe prescribed dose using the electronic keypad. 2. Press"OK" to confirm the dose and to start dosing administration. | NOTE
 | 1. Enterthe prescribed dose using the electronic keypad. 2. Press"OK" to confirm the dose and to start dosing administration. | If dosing is completed, proceed to Section 8.2.8.

8.2.6 Using Manual Dosing Mode while External Transport Mode is Enabled

This section will describe NO administration when manual ventilation is required.

ILLUSTRATION | ACTION | Warnings, Cautions and Notes
 | 1. Ensurethe oxygen flow source is set appropriately or adjust as needed. 2. Pressthe button "Switch to Manual" on the Dosing Console.
 | 1. Press "Confirm" to switch to Manual Dosing. | WARNING
 | 1. Press "Confirm" to switch to Manual Dosing. | If the dilution flow rate displayed on the screen does not match the wall source, then the estimated NO may be inaccurate.
 |  | NOTE
 |  | Dosing has been initiated at the same dose (ppm) as set in Primary Dosing Mode. If the primary dosing was set at "0" prior to pressing the "Switch to Manual" button, the estimated NO will also be at "0" and will need to be adjusted. If the dose was set between 1 and 5 ppm prior to pressing the "Switch to Manual" button, the estimated NO dose will be at "5 ppm" and may be adjusted. In the event dose is initiated in Manual Dosing Mode, the console will default to 20 ppm, which can be adjusted as needed.
 | 1. To resumeprimary dosing, see Section 8.2.7. | NOTE
 | 1. To resumeprimary dosing, see Section 8.2.7. | If an adjustment of the NO concentration is required, press the green up and down arrows. If an adjustment to the dilution flow rate is required while in Manual Dosing Mode, press the LPM value and a drop-down menu will expand. Press the prescribed value. The new value will be highlighted in blue and the drop-down menu will collapse.

8.2.7 Resuming Primary Dosing while in External Transport Mode

This section describes the process for resuming primary dosing from Manual Dosing Mode.

ILLUSTRATION | ACTION | Warnings, Cautions and Notes
 | 1. Pressthe "Switch to Primary" button at the top of the Manual Dosing Mode screen.
 | 1. Press"Confirm" to start dosing or "Cancel" to cancel. | NOTE
 | 1. Press"Confirm" to start dosing or "Cancel" to cancel. | The NO dose used in Manual Dosing Mode will become the set target dose in Primary Dosing Mode.
 |  | NOTE
 |  | The display screen will look as shown after completing steps 1-2.

8.2.8 Console Shutdown while in External Transport Mode

WARNING

NEVER turn the rear power switch OFF until the System has gone through a controlled shutdown or instructed by VERO Technical Support. Turning the rear power switch OFF prematurely (e.g., while it is still in use) will immediately shut down the device. This may result in interruption in NO delivery to the patient, which may cause injury or death.

CAUTION

NEVER turn the rear power switch OFF until the System has gone through a controlled shutdown or instructed by VERO Technical Support. Turning the rear power switch OFF prematurely (e.g., while it is still in use) will immediately shut down the device and may cause improper operation upon restart.

NOTE

- It is recommended that the Console be rebooted at least once every 30 days.
- If a Console is shutdown with External Transport Mode ON, External Transport Mode will remain ON when the Console is rebooted.

If the administration of NO must be stopped, then the dose must be set to "0". The following procedure describes how to remove the Cassettes and the following section will describe how to shut down the Console.

DISPLAY | ACTION | Warnings, Cautions and Notes
 | 1. Pressthe gray "Set" button to access the electronic keypad on the display screen.
 | 1. Setthe dose to "0" using the electronic keypad. 2. Press"OK" to confirm the entry.
 | 1. If the "Settings" tab is not displayed, pressthe "Menu" tab to access the sub-level tabs. 2. Pressthe "Settings" tab on the display menu. 3. Pressthe red "System Shutdown" icon.
 | 1. Reviewon screen prompt. 2. Press"Confirm" to shutdown Console. 3. Waituntil the Console shuts down, the display screen appears blank, and the Console emits an audible beep. | NOTE
 | 1. Reviewon screen prompt. 2. Press"Confirm" to shutdown Console. 3. Waituntil the Console shuts down, the display screen appears blank, and the Console emits an audible beep. | If the System does not shut down, see Troubleshooting Section 10.8. The screen will inform user if Cassette should be saved or disposed of. Refer to Section 2.14Shutdown Cassette Status Indicator description.
 | 1. Openlatch and Cassette Access Door.
 | 1. Removethe Cassettes by pulling the Cassette straight out and check the Cassette Status Indicator for usability 2. Savethe unused Cassette for future use. Disposethe inerted Cassette per hospital policy. | NOTE
 | 1. Removethe Cassettes by pulling the Cassette straight out and check the Cassette Status Indicator for usability 2. Savethe unused Cassette for future use. Disposethe inerted Cassette per hospital policy. | The Console will inert any remaining contents from a dosing Cassette upon ejection, rendering it unusable. If a Cassette has only been preheated, and not used for dosing, the contents have not been inerted and it can still be used. The Cassette State Window will remain blue on Cassettes that have not been inerted.
 | 1. Pressthe Black Rocker Power Switch to the "OFF" position. 2. Repeatsteps 1-13 for the other Console. | WARNING
 | 1. Pressthe Black Rocker Power Switch to the "OFF" position. 2. Repeatsteps 1-13 for the other Console. | NEVER turn the rear power switch OFF until the System has gone through a controlled shutdown or instructed by VERO Technical Support. Turning the rear power switch OFF prematurely (e.g., while it is still in use) will immediately shut down the device. This may result in interruption in NO delivery to the patient, which may cause injury or death.
 | 1. Pressthe Black Rocker Power Switch to the "OFF" position. 2. Repeatsteps 1-13 for the other Console. | CAUTION
 | 1. Pressthe Black Rocker Power Switch to the "OFF" position. 2. Repeatsteps 1-13 for the other Console. | NEVER turn the rear power switch OFF until the System has gone through a controlled shutdown or instructed by VERO Technical Support. Turning the rear power switch OFF prematurely (e.g., while it is still in use) will immediately shut down the device and may cause improper operation upon restart.

8.2.9 Switching External Transport Mode OFF

Both the Dosing Console and the Back-up Console must have External Transport Mode OFF before dosing with Hospital Cassettes in the hospital setting.

DISPLAY

ACTION

Warnings, Cautions and Notes

1. Navigateto the "Settings" tab.

1. Pressthe "External Transport Mode ON" button.

1. Select"Confirm" on the screen.

1. Enterthe external transport PIN.

NOTE

If you do not have the PIN, contact VERO Technical Support at 877.337.4118

1. ConfirmExternal Transport Mode is OFF.

GENOSYL®DS

SECTION 9
USE WITH ANESTHESIA GAS MACHINE

9. USE WITH ANESTHESIA GAS MACHINES

WARNING

- ALWAYS use the GENOSYL DS in accordance with the indications, usage, contraindications, warnings, and precautions described in the GENOSYL prescribing information and labeling. Refer to latest approved prescribing information and labeling prior to use.
- ALWAYS use the Anesthesia Gas Machine (AGM) in accordance with the manufacturer's instructions.
- The approved patient population for the GENOSYL DS as specified in the drug labeling for GENOSYL (nitric oxide for inhalation (iNO)) is limited to neonates. The GENOSYL DS is not intended to be used in other patient populations.

CAUTION

Rebreathing validation testing was performed with semi-closed breathing systems. Non-rebreathing validation testing was performed with semi-open breathing systems. The GENOSYL DS has not been evaluated with fully open or fully closed anesthesia breathing systems.

NOTE

- The GENOSYL DS performs as specified in this Operator's Manual independent of anesthetic agent, anesthetic agent concentration, and fresh gas flow rate.
- Changes in the AGM ventilator settings, fresh gas flow rate, or pushing the Oxygen Flush button by the user may cause brief transient changes in the measured NO value.
- Use of an Adaptive Sensor is recommended for use with AGMs. If not using an Adaptive Sensor:
  - And using rebreathing fresh gas flow rates, it is recommended that the < 2.5 LPM Total Flow setting be selected.
  - And using non-rebreathing fresh gas flow rates, it is recommended that the Total Flow selection based on the minute volume be selected

Compatibility testing has demonstrated performance meeting requirements for the GENOSYL DS operating range of 0 to 80 ppm with the following anesthesia gas machines at the operating ranges shown in Table 5for both mechanical and manual AGM ventilation modes. Fresh gas flow rates between 0.5 LPM and 15 LPM (10 LPM maximum tested when rebreathing), and I:E ratios ranging from 1:2 to 1:4 were validated. At low breath rates and high tidal volume settings, NO doses above 60 ppm could result in elevated NO2 levels.

See Section 12.2 Table 14for modes validated for each anesthesia gas machine.

- Drӓger Fabius GS
- Drӓger Fabius GS Premium
- Drӓger Fabius Tiro
- GE Healthcare Aisys CS2

CAUTION

- The Adaptive Sensor is recommended for use with anesthesia gas machines (AGMs). When using an AGM without the Adaptive Sensor, transient dose excursions outside of the set NO dose may occur during Cassette transition, and changes in breathing circuit flow may cause fluctuations in measured levels of NO and NO2when using the manual ventilation bag integrated with the AGM.
- When using anesthesia gas machines, NO2levels may exceed 3.0 ppm when dosing ≥ 58 ppm NO into 100% FiO2, resulting in nitric oxide delivery interruption. Once sample value of NO2is below 3.0 ppm, the Console will auto resume delivery of NO at set dose.

Table 5: Anesthesia Gas Machine Validation Compatibility Test Ranges [Inspiratory Flow Rate is not measured by Anesthesia Gas Machines.]
Setting | Range | Unit
Respiratory Rate | 6-60 | BPM
Peak Inspiratory Pressure [If testing range is higher than the max setting of the Anesthesia Gas Machine, the highest setting available was tested.] | 0-70 | cmH2O
Positive End Expiratory Pressure | 0-20 | cmH2O

Specific use cases may require the use of an Inline Mixer which is used to mix the NO gas with the gas supplied by the AGM through a filter containing silica gel to provide intra-breath NO delivery for certain scenarios. Refer to Table 6below for use case scenarios.

Table 6: Anesthesia Gas Machine Tidal Volume Use Cases
Manufacturer | Model | Fresh Gas Flow (FGF) | Ventilator Range Tested: Neonatal | Ventilator Range Tested: Pediatric/Adult
Manufacturer | Model | Fresh Gas Flow (FGF) | Ventilator Circuit Using Injection Assembly (Ref. Fig. 30) | Ventilator Circuit Using Injection Assembly (Ref. Fig. 30) | Ventilator Circuit Using Mixer Assembly (With Inline Mixer, Ref. Fig. 31)
Drӓger | Fabius GS Fabius GS Premium Fabius Tiro | FGF > 0.75 LPM | • | VT ≤ 200 ml | VT > 200-500 ml
Drӓger | Fabius GS Fabius GS Premium Fabius Tiro | FGF ≤ 0.75 LPM | • | • | N/A
GE Healthcare | Aisys CS2 | FGF > 0.75 LPM | • | VT ≤ 300 ml | VT > 300 – 585 ml
GE Healthcare | Aisys CS2 | FGF ≤ 0.75 LPM | • | • | N/A
Key
•: Range fully tested
N/A: Use of Mixer is not recommended
VT: Tidal Volume

9.1 Connection to a Dual Limb Anesthesia Circuit

The validated anesthesia circuit configurations are indicated in Table 6above and an illustrated circuit diagram is presented in Figures 30 and 31. For additional instructions on System set-up, refer to Section 3.5GENOSYL DS Gas Line Connections, Section 4System Start up, and Section 5Nitric Oxide Administration.

NOTE

Connections to various AGMS are unique to each manufacturer as well as their corresponding disposable circuits.

CAUTION

DO NOT use in environments with <20% relative humidity (RH) in the absence of supplemental humidification. Prolonged use in dry environments without humidification will damage the gas sensors. GENOSYL DS was validated with listed AGMs using a Heat Moisture Exchanger (HME) and was not tested with heated humidification connected to the respiratory circuit.

9.2 Connection Instructions for the GENOSYL DS to an Anesthesia Gas Machine

WARNING

- The flow out of the anesthesia gas machine via the INSPIRATORY breathing circuit limb must pass through the GENOSYL DS Gas Injection Assembly.
- The GENOSYL DS injects and samples gas from the patient respiratory circuit which may affect the triggering sensitivity of the anesthesia gas machine (AGM). ALWAYS ensure the trigger sensitivity of the AGM is checked after connecting the GENOSYL DS to the breathing circuit and starting iNO delivery or when the dose is changed and adjust trigger sensitivity as necessary. Failure to do so may lead to AGM auto cycling or apnea alarm.
- ALWAYS ensure the patient disconnect and high–pressure alarms are used with the AGM.

NOTE

- A dual limb anesthesia breathing circuit should be used for iNO delivery with the GENOSYL DS.
- The GENOSYL DS Sample Line must be placed on the INSPIRATORY limb of the breathing circuit between 6 and 12 inches from the patient wye. If the sampling line is placed greater than 6 inches from the patient wye it minimizes the sampling of mixed inspired/expired gas concentrations and if placed less than 12 inches from the patient wye it ensures correct iNO and NO2measurement.

DISPLAY | ACTION | Warnings, Cautions and Notes
 | 1. Connectthe Inline Breathing Circuit Filter to the Gas Injection Adapter (22 mm ID × 22 mm OD). 2. Connectthe Adaptive Sensor to the inlet end of Gas Injection Adapter (22mm ID × 22 MM OD). | NOTE
 | 1. Connectthe Inline Breathing Circuit Filter to the Gas Injection Adapter (22 mm ID × 22 mm OD). 2. Connectthe Adaptive Sensor to the inlet end of Gas Injection Adapter (22mm ID × 22 MM OD). | For detailed Injection Assembly with Adaptive Sensor instructions, refer to Section 3.4.1. If an Inline Mixer is required per Table 6,refer to Section 3.4.2for instructions to assemble and then proceed to Step 2.
 | 1. Attachthe Injection Assembly with Adaptive Sensor to the Gas Injection Adapter on the Inspiratory Port on the AGM.
 | 1. Attachthe inspiratory limb of the breathing circuit to the Inline Breathing Circuit Filter. If the breathing circuit has a Sample Gas Tee inserted, ensure this limb of the circuit is attached to the Inline Breathing Circuit Filter.
 | 1. Insertthe Gas Sample Tee into the inspiratory limb of the breathing circuit, 6-12" from the patient wye. | WARNING
 | 1. Insertthe Gas Sample Tee into the inspiratory limb of the breathing circuit, 6-12" from the patient wye. | Ensure the Injection Assembly and the Gas Sample Tee are BOTH inserted on the inspiratory limb of the circuit.
 | 1. Insertthe Gas Sample Tee into the inspiratory limb of the breathing circuit, 6-12" from the patient wye. | NOTE
 | 1. Insertthe Gas Sample Tee into the inspiratory limb of the breathing circuit, 6-12" from the patient wye. | Skip this step if a Gas Sample Tee is already connected and in-line with the circuit.
 | 1. Insertan Inline Breathing Circuit Filter between the Expiratory Port and expiratory limb. Skip this step if a bacterial filter is already present in the expiratory limb of the breathing circuit. | NOTE
 | 1. Insertan Inline Breathing Circuit Filter between the Expiratory Port and expiratory limb. Skip this step if a bacterial filter is already present in the expiratory limb of the breathing circuit. | Skip this step if a bacteria filter is already connected and in-line with the circuit.
 | 1. Attachthe expiratory limb of the breathing circuit to the Inline Breathing Circuit Filter on the Expiratory Port on the Anesthesia Machine
 | 1. Push and twistclockwise the luerlock collar from the NO injection line onto the NO injection port of the Gas Injection Adapter on the Injection Assembly.
 | 1. Push andtwistclockwise the Luer-Lock Collar of the Stopcock on the Sample Line onto the Sampling Port of the Gas Sample Tee. | NOTE
 | 1. Push andtwistclockwise the Luer-Lock Collar of the Stopcock on the Sample Line onto the Sampling Port of the Gas Sample Tee. | Refer to Section 4for Console Start up instructions and Section 5for nitric oxide administration instructions.
 | 1. Connectthe distal end of the Adaptive Sensor Cable to the Adaptive Sensor on the Injection Assembly
 | 1. Refer to Section 3.6for connection instructions of the GENOSYL DS to a manual bagging system.

NOTE

- When using the manual ventilation bag integrated with the AGM, nitric oxide can be delivered by leaving the Console in Primary Dosing Mode. Nitric oxide will be delivered through the Injection Assembly into the anesthesia gas circuit.
- In the event of anesthesia gas machine failure, NO delivery can be continued using Manual Dosing Mode on the GENOSYL DS with a manual bag connected to the manual ventilation port on the front of the Console and an alternative gas source than the AGM. Refer to Section 3.6for GENOSYL DS connection instructions and Section 5.4for GENOSYL DS Manual Dosing Mode operating instructions.

GENOSYL®DS

SECTION 10
ALARMS, ALERTS, AND TROUBLESHOOTING

10. ALARMS, ALERTS, AND TROUBLESHOOTING

WARNING

ALWAYS ensure patient safety before troubleshooting (such as an activated alarm) or replacing a problematic item. Not monitoring the patient prior to attending to an alarm can result in injury or death.

10.1 Alarms, Alerts, and Troubleshooting

This section contains the System alarms and messages in order of High (red), Medium (yellow), and Low Priority (turquoise) followed by Informational Messages (green). The table shows the alarm/symptom, the possible cause(s) of the alarm and recommended action to resolve the alarm. If the alarm/issue cannot be resolved, contact Technical Support at 877-337-4118.

A sample screen with an active alarm is shown below:

The alarm banner contains a drop-down menu containing a list of all alarms should there be multiple activated. Tapping the alarm banner will open the VERO On-screen Troubleshooting module (See Section 10.2). The alarm icon is always present on the top right of the screen and tapping the icon will pre-silence or silence alarms. Refer to the table below for descriptions of each alarm status:

Table 7: Alarm Icon Descriptions
ALARM ICON DISPLAY | DESCRIPTION
 | No active alarm condition is detected on the Console. Tap this icon to activate the Pre-Silence feature.
 | Alarms are actively pre-silenced. Countdown of time remaining appears under the icon. Pre-silence lasts for 120 seconds. Low/High NO, High NO2, Low/High O2, Water Trap Removed, and Dosing Cassette Removed alarms are pre-silenced. Alarms will still be visible on alarm banner but audible alarm will not sound.
 | Console has an active alarm condition that requires attention. Tap the icon to silence the alarm for 120 seconds.
 | Console has an active alarm condition that requires attention and the alarms have been silenced. Countdown of time remaining for silence appears on bottom of icon.

The alarm order, color, and audio signal will follow the highest priority alarm.

Table 8: Alarm Characteristics
Alarm Priority | Color | Flashing Frequency | Flashing Duty Cycle | Sound Level
High | Red | 1.4 to 2.8 Hz | 40-60% | 79.8 dBA
Medium | Yellow | 0.4 to 0.8 Hz | 40-60% | 76.1 dBA
Low | Turquoise | Constant (on) | 100% | 63.3 dBA

Some alarms may be adjusted within the "Alarms" tab. See Table 9below for adjustment characteristics. The System will always resort to the original default alarm settings upon reboot or complete power failure.

In addition, the System has a fallback safety dose interruption feature which will temporarily interrupt delivery of NO when the sensors detect a sampled value of ≥ 100 ppm NO and/or ≥ 3 ppm NO2. The System will resume NO dosing after dissipation of high gases without operator input.

Review Table 9for complete details about the alarm adjustment ranges, defaults, alarm activation timing and interruption conditions.

Table 9: Alarm Ranges, Defaults and Dose Interruption Condition
Alarm | Adjustment Range | Default Setting | Alarm Activation | Interruption Condition
High NO (ppm) | 0 – 100 ppm | + 50% of set value or 2 ppm (Whichever is greater) | 10 minutes after dose >0 ppm entered | ≥ 100 ppm
Low NO (ppm) | 0 – 99 ppm | - 50% of set point. For doses less than 4ppm, setting ranges between -50 - 70% of set point | 10 minutes after dose >0 ppm entered | NA
High NO2(ppm) | 1-2.9 ppm | 2 ppm | 30 seconds after dose > 0 ppm entered | ≥ 3 ppm
High O2(% v/v) | 22 – 100 ppm | 100 ppm | Immediately after dose > 0 ppm entered | N/A
Low O2(% v/v) | 18 – 99 ppm | 18 ppm | Immediately after dose > 0 PPM entered | N/A

NOTE

The safety dose interruption feature is active immediately upon setting a dose greater than 0 ppm. The NO and NO2alarms do not need to be active for the safety dose interruption feature to be activated.

Alarms are legible for a person with 20/20 vision at a distance of 1 meter when viewed directly on the screen.

An alarm history indicating the date, time, and type of alarm can be viewed by selecting the "Alarms" tab and then selecting the alarms history button. The alarm history can be cleared by pressing the "Clear Alarm" button. If the alarm history reaches capacity, the oldest alarms will begin rolling off and become non-visible to the user. Upon Console shut down or power loss, the alarm log is cleared. If the alarm log is cleared, or reaches capacity, history of alarms will still be recorded in permanent memory accessible when logged in as admin. The operator of the equipment should be physically in front of the Console while interacting with the System. During NO delivery, the operator should remain within visual and auditory distance of the System.

The alarm system is automatically tested during the initial power-on self-test with an audible beep to confirm successful completion. Should there be an issue with communication to the alarms system electronics, a Hardware Failure error message will appear at the end of the self-test.

10.2 On-screen Troubleshooting Module

The GENOSYL DS features on-screen troubleshooting support for specific alarm conditions (refer to Table 10for a list of alarms where on-screen troubleshooting support is available). This module can be accessed by tapping an active alarm banner or by selecting the "Alarm Info" button on the "Alarms" tab. If no alarm condition is active, and the module is accessed via the "Alarms" tab, a menu will be presented to select which condition the user would like to view troubleshooting steps for. Refer to Figure 32for a view of the menu. If an alarm condition is active, the module will open directly to recommended troubleshooting actions, if available. Refer to Figure 33for a description of navigating the module. If the user cannot address the alarm condition using the module, the user will be instructed to consider switching to the Back-up Console and should contact Technical Support.

Table 10: Alarm conditions included in On-screen Troubleshooting Module

Alarm Condition

Low NO

Line Occlusion

Delivery Flow Error

High Back Pressure

1. Recommend action to address alarm condition
2. Question to confirm if recommended action addressed active alarm condition.
3. Yes/No to answer if recommended action addressed alarm condition. Pressing "Yes" will exit the module. Pressing "No" will advance to the next recommended action.
4. "Exit" button will exit the module.
5. "Back" button will bring user to the previous screen (previous recommended action).
6. NO and NO2values will display on this portion of the screen.

Figure 33: Description of VERO On-screen Troubleshooting Module Navigation

10.3 High Priority Alarms and Messages

High priority alarms and messages will have a red background and be accompanied by an audible alarm. These alarms and messages require immediate operator response.

High Priority Alarms and Messages
Alarm/Message | Possible Cause | Recommended Action
Nitric Oxide Delivery Interruption due to High NO Message Box: | - Respiratory circuit flow changed abruptly - Low or no flow - in patient respiratory circuit - Condensation - Cause not determined | This fallback mode will be cancelled once the nitric oxide level drops below the set dose + 50%.; 1. Verify flow is present in the patient's respiratory circuit. 2. Allow time for the sensor measurement to adjust while completing the next steps. 3. Verify GENOSYL DS gas line connections are tight by loosening then retightening each connection on the red injection and blue sample lines. 4. Verify proper placement of injection assembly and sample adapter within the respiratory circuit. 5. Replace adapters that have evidence of excessive condensation. 6. If the sensor measurement does not adjust, switch to Back-up Console. 7. Contact Technical Support.
Banner: | - Respiratory circuit flow changed abruptly - Low or no flow - in patient respiratory circuit - Condensation - Cause not determined | This fallback mode will be cancelled once the nitric oxide level drops below the set dose + 50%.; 1. Verify flow is present in the patient's respiratory circuit. 2. Allow time for the sensor measurement to adjust while completing the next steps. 3. Verify GENOSYL DS gas line connections are tight by loosening then retightening each connection on the red injection and blue sample lines. 4. Verify proper placement of injection assembly and sample adapter within the respiratory circuit. 5. Replace adapters that have evidence of excessive condensation. 6. If the sensor measurement does not adjust, switch to Back-up Console. 7. Contact Technical Support.
Screen Display: | - Respiratory circuit flow changed abruptly - Low or no flow - in patient respiratory circuit - Condensation - Cause not determined | This fallback mode will be cancelled once the nitric oxide level drops below the set dose + 50%.; 1. Verify flow is present in the patient's respiratory circuit. 2. Allow time for the sensor measurement to adjust while completing the next steps. 3. Verify GENOSYL DS gas line connections are tight by loosening then retightening each connection on the red injection and blue sample lines. 4. Verify proper placement of injection assembly and sample adapter within the respiratory circuit. 5. Replace adapters that have evidence of excessive condensation. 6. If the sensor measurement does not adjust, switch to Back-up Console. 7. Contact Technical Support.
Nitric Oxide Delivery Interruption due to High NO2 Message Box: | - Low or no flow in patient respiratory circuit - Respiratory flow changed abruptly - Leak in patient respiratory circuit - Condensation - Bias flow on respiratory device is too low - Cause not determined | This fallback mode will be cancelled once the NO2 level drops below 3 ppm.; 1. Verify flow is present in patient's respiratory circuit. 2. Consider increasing bias flow, if applicable. 3. Allow time for the sensor measurement to adjust while completing the next steps. 4. Verify GENOSYL DS gas line connections are tight by loosening then retightening each connection on the red injection and blue sample lines. 5. Verify proper placement of injection assembly and sample adapter within the respiratory circuit. 6. Replace adapters that have evidence of excessive condensation. 7. If the sensor measurement does not adjust, switch to Back-up Console. 8. Contact Technical Support.
Banner: | - Low or no flow in patient respiratory circuit - Respiratory flow changed abruptly - Leak in patient respiratory circuit - Condensation - Bias flow on respiratory device is too low - Cause not determined | This fallback mode will be cancelled once the NO2 level drops below 3 ppm.; 1. Verify flow is present in patient's respiratory circuit. 2. Consider increasing bias flow, if applicable. 3. Allow time for the sensor measurement to adjust while completing the next steps. 4. Verify GENOSYL DS gas line connections are tight by loosening then retightening each connection on the red injection and blue sample lines. 5. Verify proper placement of injection assembly and sample adapter within the respiratory circuit. 6. Replace adapters that have evidence of excessive condensation. 7. If the sensor measurement does not adjust, switch to Back-up Console. 8. Contact Technical Support.
Screen Display: | - Low or no flow in patient respiratory circuit - Respiratory flow changed abruptly - Leak in patient respiratory circuit - Condensation - Bias flow on respiratory device is too low - Cause not determined | This fallback mode will be cancelled once the NO2 level drops below 3 ppm.; 1. Verify flow is present in patient's respiratory circuit. 2. Consider increasing bias flow, if applicable. 3. Allow time for the sensor measurement to adjust while completing the next steps. 4. Verify GENOSYL DS gas line connections are tight by loosening then retightening each connection on the red injection and blue sample lines. 5. Verify proper placement of injection assembly and sample adapter within the respiratory circuit. 6. Replace adapters that have evidence of excessive condensation. 7. If the sensor measurement does not adjust, switch to Back-up Console. 8. Contact Technical Support.
High NO Alarm Message Box: None | - Respiratory circuit flow changed abruptly - Low or no flow in patient respiratory circuit - High NO alarm may be inappropriately set - Condensation - Cause not determined | 1. Verify flow is present in the patient's respiratory circuit. 2. Allow time for the sensor measurement to adjust while completing the next steps. 3. Verify GENOSYL DS gas line connections are tight by loosening then retightening each connection on the red injection and blue sample lines. 4. Verify proper placement of injection assembly and sample adapter within the respiratory circuit. 5. Replace adapters that have evidence of excessive condensation. 6. Go to the Alarms screen and check the NO alarm setting. Set alarm to the desired setting. 7. If the sensor measurement does not adjust, switch to Back-up Console. 8. Contact Technical Support.
Banner: | - Respiratory circuit flow changed abruptly - Low or no flow in patient respiratory circuit - High NO alarm may be inappropriately set - Condensation - Cause not determined | 1. Verify flow is present in the patient's respiratory circuit. 2. Allow time for the sensor measurement to adjust while completing the next steps. 3. Verify GENOSYL DS gas line connections are tight by loosening then retightening each connection on the red injection and blue sample lines. 4. Verify proper placement of injection assembly and sample adapter within the respiratory circuit. 5. Replace adapters that have evidence of excessive condensation. 6. Go to the Alarms screen and check the NO alarm setting. Set alarm to the desired setting. 7. If the sensor measurement does not adjust, switch to Back-up Console. 8. Contact Technical Support.
Screen Display: | - Respiratory circuit flow changed abruptly - Low or no flow in patient respiratory circuit - High NO alarm may be inappropriately set - Condensation - Cause not determined | 1. Verify flow is present in the patient's respiratory circuit. 2. Allow time for the sensor measurement to adjust while completing the next steps. 3. Verify GENOSYL DS gas line connections are tight by loosening then retightening each connection on the red injection and blue sample lines. 4. Verify proper placement of injection assembly and sample adapter within the respiratory circuit. 5. Replace adapters that have evidence of excessive condensation. 6. Go to the Alarms screen and check the NO alarm setting. Set alarm to the desired setting. 7. If the sensor measurement does not adjust, switch to Back-up Console. 8. Contact Technical Support.
High NO2Alarm Message Box: None | - Low or no flow in patient respiratory circuit - Respiratory circuit flow changed abruptly - High NO2alarm may be inappropriately set - Condensation - Bias flow on respiratory device is too low - Cause not determined | 1. Verify flow is present in the patient's respiratory circuit. 2. Consider increasing bias flow, if applicable 3. Allow time for the sensor measurement to adjust while completing the next steps. 4. Verify GENOSYL DS gas line connections are tight by loosening then retightening each connection on the red injection and blue sample lines. 5. Verify proper placement of injection assembly and sample adapter within the respiratory circuit. 6. Replace adapters that have evidence of excessive condensation. 7. Go to the Alarms screen and check the NO2 alarm setting. Set alarm to the desired setting. 8. If the sensor measurement does not adjust, switch to Back-up Console 9. Contact Technical Support
Banner: | - Low or no flow in patient respiratory circuit - Respiratory circuit flow changed abruptly - High NO2alarm may be inappropriately set - Condensation - Bias flow on respiratory device is too low - Cause not determined | 1. Verify flow is present in the patient's respiratory circuit. 2. Consider increasing bias flow, if applicable 3. Allow time for the sensor measurement to adjust while completing the next steps. 4. Verify GENOSYL DS gas line connections are tight by loosening then retightening each connection on the red injection and blue sample lines. 5. Verify proper placement of injection assembly and sample adapter within the respiratory circuit. 6. Replace adapters that have evidence of excessive condensation. 7. Go to the Alarms screen and check the NO2 alarm setting. Set alarm to the desired setting. 8. If the sensor measurement does not adjust, switch to Back-up Console 9. Contact Technical Support
Screen Display: | - Low or no flow in patient respiratory circuit - Respiratory circuit flow changed abruptly - High NO2alarm may be inappropriately set - Condensation - Bias flow on respiratory device is too low - Cause not determined | 1. Verify flow is present in the patient's respiratory circuit. 2. Consider increasing bias flow, if applicable 3. Allow time for the sensor measurement to adjust while completing the next steps. 4. Verify GENOSYL DS gas line connections are tight by loosening then retightening each connection on the red injection and blue sample lines. 5. Verify proper placement of injection assembly and sample adapter within the respiratory circuit. 6. Replace adapters that have evidence of excessive condensation. 7. Go to the Alarms screen and check the NO2 alarm setting. Set alarm to the desired setting. 8. If the sensor measurement does not adjust, switch to Back-up Console 9. Contact Technical Support
Low NO alarm Message Box: None | - Gas lines are not connected or properly placed in the respiratory circuit - Water Trap full - Leak in respiratory circuit - Cassette not full inserted - Alarm limit not adjusted properly - NO Cassette needs to be replaced - Cassette is depleted without a second Cassette inserted - Gas sample tee placed too close to patient wye adapter - Cause not determined | 1. Verify GENOSYL DS gas line connections are tight by loosening then retightening each connection on the red injection and blue sample lines. 2. Verify proper placement of Injection Assembly and Sample adapter within the respiratory circuit. 3. Ensure gas sample tee is placed 6 to 12 inches from the patient wye adapter. 4. Replace adapters that have evidence of excessive condensation. 5. Check the respiratory circuit for the presence of leaks. 6. If not using an Adaptive Sensor, confirm total flow range is properly selected. 7. Allow time for the sensor measurement to adjust while completing the next steps. 8. Push on Cassette to ensure it is fully seated. 9. Empty Water Trap. Replace Water Trap if necessary. 10. If Cassette is depleted, insert a second Cassette if not already present. If auto transition does not occur, switch to Back-up Console. 11. Ensure dose and flow are set within specifications. (see Section 12.1.4Liters per minute multiplied by ppm should not exceed 800. (Example 40 LPM × 20ppm = 800) 12. Go to alarms screen and check the NO alarm setting. Set the alarm to the desired setting. 13. If sensor measurement does not adjust, switch over to Back-up Console. 14. Contact Technical Support.
Banner: | - Gas lines are not connected or properly placed in the respiratory circuit - Water Trap full - Leak in respiratory circuit - Cassette not full inserted - Alarm limit not adjusted properly - NO Cassette needs to be replaced - Cassette is depleted without a second Cassette inserted - Gas sample tee placed too close to patient wye adapter - Cause not determined | 1. Verify GENOSYL DS gas line connections are tight by loosening then retightening each connection on the red injection and blue sample lines. 2. Verify proper placement of Injection Assembly and Sample adapter within the respiratory circuit. 3. Ensure gas sample tee is placed 6 to 12 inches from the patient wye adapter. 4. Replace adapters that have evidence of excessive condensation. 5. Check the respiratory circuit for the presence of leaks. 6. If not using an Adaptive Sensor, confirm total flow range is properly selected. 7. Allow time for the sensor measurement to adjust while completing the next steps. 8. Push on Cassette to ensure it is fully seated. 9. Empty Water Trap. Replace Water Trap if necessary. 10. If Cassette is depleted, insert a second Cassette if not already present. If auto transition does not occur, switch to Back-up Console. 11. Ensure dose and flow are set within specifications. (see Section 12.1.4Liters per minute multiplied by ppm should not exceed 800. (Example 40 LPM × 20ppm = 800) 12. Go to alarms screen and check the NO alarm setting. Set the alarm to the desired setting. 13. If sensor measurement does not adjust, switch over to Back-up Console. 14. Contact Technical Support.
Calibration Required Message Box: | - Calibration for the sensor is required | This fallback mode will be cancelled once a successful high gas calibration has been completed.; 1. Calibrate Console (see Section 11.1). 2. If the calibration required alarm occurs after a successful calibration has been completed, contact Technical Support.
Banner: | - Calibration for the sensor is required | This fallback mode will be cancelled once a successful high gas calibration has been completed.; 1. Calibrate Console (see Section 11.1). 2. If the calibration required alarm occurs after a successful calibration has been completed, contact Technical Support.
Hardware Failure Message Box: | - Internal hardware damage or communication failure | In this fallback mode, the Console will continue delivering nitric oxide in an open loop mode at the last entered dose.; 1. Switch to Back-up Console. 2. Contact Technical Support.
Banner: | - Internal hardware damage or communication failure | In this fallback mode, the Console will continue delivering nitric oxide in an open loop mode at the last entered dose.; 1. Switch to Back-up Console. 2. Contact Technical Support.
Hardware Failure – Power Board Message Box: | - Internal hardware damage or communication failure | 1. Switch to Back-up Console. 2. Contact Technical Support.
Banner: | - Internal hardware damage or communication failure | 1. Switch to Back-up Console. 2. Contact Technical Support.
Hardware Error During POST (Power On Self-Test) Message Box: | - Problem occurring during boot-up sequence - Internal hardware damage or communication failure | 1. Use Back-up Console if NO delivery is needed immediately. 2. Re-boot by holding Silver Power Button down for 10 seconds. 3. If error message continues, contact Technical Support.
Battery Error Message Box: None | - Internal battery error or battery fails to charge - Battery becomes disconnected | 1. Plug in AC power. 2. Verify power connections on Console, power adapters, and AC power source. 3. Verify the light on the black power supply is illuminated and green. 4. If not dosing, shut down Console. 5. Allow Console to charge for a minimum of 1 hour. Monitor the Charge Status Indicator on the front panel. Indicator should charge from red to green when the battery has achieved enough charge to resolve the battery error. 6. Restart Console and verify if error persists. 7. If error persists, allow battery to charge several more hours, or overnight. 8. If alarm does not clear, switch to Back-up Console and contact Technical Support
Banner: | - Internal battery error or battery fails to charge - Battery becomes disconnected | 1. Plug in AC power. 2. Verify power connections on Console, power adapters, and AC power source. 3. Verify the light on the black power supply is illuminated and green. 4. If not dosing, shut down Console. 5. Allow Console to charge for a minimum of 1 hour. Monitor the Charge Status Indicator on the front panel. Indicator should charge from red to green when the battery has achieved enough charge to resolve the battery error. 6. Restart Console and verify if error persists. 7. If error persists, allow battery to charge several more hours, or overnight. 8. If alarm does not clear, switch to Back-up Console and contact Technical Support
Line Occlusion (Sample) Message Box: None | - Stopcock valve on the Sample Line (blue) is in the closed position - Water Trap is full - Blue Sample Line is kinked or occluded - Sample Line Filter is occluded - Cause not determined | In this fallback mode, the Console will continue delivering nitric oxide in an open loop mode at the last commanded dose until the line occlusion is resolved.; 1. Ensure blue Sample Line Stopcock is in the open position. 2. Remove Sample Line Filter, replace if needed. 3. Empty Water Tap. 4. If occlusion persists after emptying, replace Water Trap. 5. Inspect entire length of blue sample line for kinks or occlusions. 6. Replace gas lines if kink or occlusion cannot be resolved. 7. If issue is still not resolved, switch over to Back-up Console. 8. Contact Technical Support.
Banner: | - Stopcock valve on the Sample Line (blue) is in the closed position - Water Trap is full - Blue Sample Line is kinked or occluded - Sample Line Filter is occluded - Cause not determined | In this fallback mode, the Console will continue delivering nitric oxide in an open loop mode at the last commanded dose until the line occlusion is resolved.; 1. Ensure blue Sample Line Stopcock is in the open position. 2. Remove Sample Line Filter, replace if needed. 3. Empty Water Tap. 4. If occlusion persists after emptying, replace Water Trap. 5. Inspect entire length of blue sample line for kinks or occlusions. 6. Replace gas lines if kink or occlusion cannot be resolved. 7. If issue is still not resolved, switch over to Back-up Console. 8. Contact Technical Support.
Line Occlusion (Cal) Message Box: None | - Obstruction to calibration port - Calibration tank valve closed during high calibration procedure - Cause not determined | 1. Ensure calibration port is free of debris or damage and nothing is connected. 2. Perform high calibration by following procedure in Section 11.1 3. If issue is still not resolved, switch over to Back-up Console. 4. Contact Technical Support
Banner: | - Obstruction to calibration port - Calibration tank valve closed during high calibration procedure - Cause not determined | 1. Ensure calibration port is free of debris or damage and nothing is connected. 2. Perform high calibration by following procedure in Section 11.1 3. If issue is still not resolved, switch over to Back-up Console. 4. Contact Technical Support
Cassette Removed while dosing Message Box: | - Cassette manually ejected using emergency ejection tabs - Hardware damage which causes the System to not be able to detect the Cassette - Cause not determined | 1. If secondary Cassette is not inserted, transition to Back-up Console 2. Contact Technical Support.
Banner: None | - Cassette manually ejected using emergency ejection tabs - Hardware damage which causes the System to not be able to detect the Cassette - Cause not determined | 1. If secondary Cassette is not inserted, transition to Back-up Console 2. Contact Technical Support.
Water Trap Not Detected Message Box: | - Water Trap not seated properly - Water Trap not present - Cause not determined | In this fallback mode, the console will continue delivering nitric oxide in an open loop mode at the last commanded dose until the water trap is replaced and the leak check is passed.; 1. Re-seat Water Trap. 2. Insert new Water Trap. 3. Switch over to Back-up Console. 4. Contact Technical Support.
Banner: | - Water Trap not seated properly - Water Trap not present - Cause not determined | In this fallback mode, the console will continue delivering nitric oxide in an open loop mode at the last commanded dose until the water trap is replaced and the leak check is passed.; 1. Re-seat Water Trap. 2. Insert new Water Trap. 3. Switch over to Back-up Console. 4. Contact Technical Support.
Configuration Parameters Incorrect Message Box: | - File integrity issue | 1. Use Back-up Console if NO delivery is needed immediately. 2. Contact Technical Support.
Battery Not Detected during POST (Power On Self- Test) Message Box: | - Battery is not connected properly or not operational | 1. Use Back-up Console if NO delivery is needed immediately. 2. Contact Technical Support.
Hardware Error During POST (Power On Self-Test) Message Box: | - Hardware failure occurred | 1. Use Back-up Console if NO delivery is needed immediately. 2. Contact Technical Support.
Banner: | - Hardware failure occurred | 1. Use Back-up Console if NO delivery is needed immediately. 2. Contact Technical Support.
Cassette Not Operational Message Box: | - Hardware failure within Cassette during dosing | If a secondary Cassette is inserted in the other slot, the Console will automatically switch to the secondary Cassette in this fallback mode.; 1. If a secondary Cassette is not inserted in the other slot, switch to Back-up Console. 2. Replace Cassette in original Dosing Console 3. If issue is not resolved, switch to Back-up Console. 4. Contact Technical Support.
System has not Completed Calibration | - Calibration was not completed - Wrong/empty calibration gas tank used - Calibration tubing is incorrectly connected to the sample port - Failed Gas Sensor - Calibration tank does not have enough PSI - Kink or occlusion in calibration tubing. - Break or crack in calibration tubing or cal gas tee - Calibration tubing is incorrectly connected to the sample port. - Calibration regulator is missing a washer. | 1. Accept message. 2. Obtain correct/full calibration gas tank. 3. Verify there is adequate gas present in cal tank to complete calibration (>500 PSI). 4. Connect calibration tubing to Cal port. 5. Verify the cal gas extension line and gas tee are free from breaks, cracks, kinks or occlusions. 6. Verify presence of washer and that it is properly seated between calibration. 7. Perform gas calibration. See Calibration Section 11.1. 8. If you continue to have problems, contact Technical Support.
Hardware Failure while Dosing in Manual Dosing Mode – No Dose Change Message Box: | - Internal hardware damage or communication failure | In this fallback mode, the Console will continue delivering nitric oxide in an open loop mode at the last entered dose. User will not be able to adjust set dose.; 1. Switch to Back-up Console. 2. Contact Technical Support.
Banner: | - Internal hardware damage or communication failure | In this fallback mode, the Console will continue delivering nitric oxide in an open loop mode at the last entered dose. User will not be able to adjust set dose.; 1. Switch to Back-up Console. 2. Contact Technical Support.
Hardware Failure while Dosing–Cannot Change Dosing Modes Message Box: | - Internal hardware damage or communication failure | In this fallback mode, the Console will continue delivering nitric oxide in an open loop mode at the last entered dose. User will not be able to switch between Dosing Modes (Primary and Manual Dosing Mode); 1. Switch to Back-up Console. 2. Contact Technical Support.
Banner: | - Internal hardware damage or communication failure | In this fallback mode, the Console will continue delivering nitric oxide in an open loop mode at the last entered dose. User will not be able to switch between Dosing Modes (Primary and Manual Dosing Mode); 1. Switch to Back-up Console. 2. Contact Technical Support.

10.4 Medium Priority Alarms and Messages

Medium priority alarms and messages will have a yellow background. Medium priority alarms and messages require a prompt response from the operator.

Medium Priority Alarms and Messages
Alarm/Message | Possible Cause | Recommended Action
Low Battery Alarm Message box: None Banner: | - Battery is low | 1. Verify power connections on console, power adapters, and AC power source. 2. If AC power is not available, switch to Back-up Console. 3. Then plug into AC power as soon as possible.
Cassette Failure Alarm | - Internal Cassette issue | 1. Replace with a new Cassette. 2. If unresolved, switch to Back-up Console and contact Technical Support.
Service Due Date Expired | - Service date is past due | 1. Accept message. 2. To schedule service, contact Technical Support. 3. Schedule every 24 months.
Cassette to Expire in 1 Hour | - Cassette will deplete in 1 hour | 1. Ensure secondary Cassette is inserted and ready. 2. Replace Cassette once transition is complete.
Low O2 Message box: none Banner: | - Respiratory device setting is incorrect - Alarm setting is incorrect - Ventilator flow is too low | 1. Verify respiratory device setting is correct. 2. Set the alarm ranges to the correct setting. 3. Calibrate Console (see Section 11.1). 4. If sensor measurement does not adjust, switch over to Back-up Console. 5. Contact Technical Support.
High O2 Message Box: none Banner: | - Respiratory device setting is incorrect - Alarm setting is incorrect | 1. Verify respiratory device setting is correct. 2. Set the alarm ranges to the correct setting. 3. Calibrate Console (see Section 11.1). 4. If sensor measurement does not adjust, switch over to Back-up Console. 5. Contact Technical Support.
Delivery Flow Error Message Box: | - Red injection line is kinked or occluded - Kink or occlusion in respiratory circuit - NO port is occluded - Excess pressure in respiratory circuit - Hardware issue caused a failure | 1. Inspect entire length of red injection line for kinks and occlusions. 2. Insect respiratory circuit for kinks or occlusions 3. Inspect NO output port on front of console for debris or damage. 4. Ensure the air intake is not blocked. 5. Resolve the kink or blockage. 6. If in Manual Dosing Mode, ensure flow to patient matches selected flow on GENOSYL. 7. If problem persists, contact Technical Support.
Banner: | - Red injection line is kinked or occluded - Kink or occlusion in respiratory circuit - NO port is occluded - Excess pressure in respiratory circuit - Hardware issue caused a failure | 1. Inspect entire length of red injection line for kinks and occlusions. 2. Insect respiratory circuit for kinks or occlusions 3. Inspect NO output port on front of console for debris or damage. 4. Ensure the air intake is not blocked. 5. Resolve the kink or blockage. 6. If in Manual Dosing Mode, ensure flow to patient matches selected flow on GENOSYL. 7. If problem persists, contact Technical Support.
High Back Pressure Message Box: | - Kinks or occlusions in the respiratory circuit. | 1. Inspect respiratory circuits for kinks or occlusions. 2. Resolve the kink or blockage. 3. If problem persists, contact Technical Support.
Banner: | - Kinks or occlusions in the respiratory circuit. | 1. Inspect respiratory circuits for kinks or occlusions. 2. Resolve the kink or blockage. 3. If problem persists, contact Technical Support.
Incorrect Cassette Message Box: | - External Transport Cassette has been inserted while External Transport Mode is OFF. | 1. Identify if the intended environment is Hospital or External Transport. 2. If Hospital, insert Hospital Cassette to dose. 3. If External Transport, turn External Transport ON. See Section 8.2.1. 4. If problem persists, contact Technical Support.
Incorrect Cassette Message Box: | - Hospital Cassette has been inserted while External Transport Mode is ON. | 1. Identify if the intended environment is Hospital or External Transport. 2. If Hospital, turn External Transport OFF. See Section 8.2.9. 3. If External Transport, insert External Transport Cassette to dose. 4. If problem persists, contact Technical Support.

10.5 Low Priority Alarms and Messages

A low priority message will have a turquoise background. A low priority message will require that the operator is aware of the condition.

Low Priority Messages and Alarms
Alarm/Message | Possible Cause | Recommended Action
Nitric Oxide Delivery Interruption due to Flow Not Detected Message Box: | - Adaptive Sensor not detecting flow - Cause not determined | Once flow is detected through the Adaptive Sensor, dosing will resume automatically and this fallback mode will be cancelled.; 1. Verify proper connection of Adaptive Sensor to respiratory circuit 2. Verify flow is present in the respiratory circuit
Screen Display: | - Adaptive Sensor not detecting flow - Cause not determined | Once flow is detected through the Adaptive Sensor, dosing will resume automatically and this fallback mode will be cancelled.; 1. Verify proper connection of Adaptive Sensor to respiratory circuit 2. Verify flow is present in the respiratory circuit
System Running on Battery Only | - AC power is not connected | 1. Check the AC power connection. 2. Verify power connections on Console, power adapters, and AC power source. 3. If connecting to AC power does not resolve issue, switch to Back-up Console and contact Technical Support.
Service Due Date Within 2 Days | - Service date is scheduled within 2 days | 1. Accept message. 2. Contact Technical Support to have System serviced at earliest convenience.

10.6 Informational Messages

Informational messages will have a green background. These messages require that the user is notified of the condition.

Informational Messages
Alarm/Message | Possible Cause | Recommended Action
Calibration Due within 48 Hours | - Calibration is required within 48 hours | 1. Accept message. 2. Perform gas calibration if desired. See Calibration Section 11.1.
Service Due Date Within 14 Days | - Service date is scheduled within - 14 days | 1. Accept message. 2. Contact Technical Support to have System serviced at your convenience.
Cassette Will Expire In 2 Hours | - Cassette will expire within 2 hours and no secondary Cassette inserted | 1. Insert secondary Cassette. 2. Replace Cassette once transition is complete.
Calibration Due | - Calibration due date has passed | 1. Perform gas calibration. See Calibration Section 11.1.
Invalid External Transport password | - Invalid External Transport password | 1. Input correct password. 2. If problem persists, contact Technical Support.
Turn External Transport Mode ON | - Confirm External Transport Mode is ON | 1. Press "Confirm" to turn External Transport Mode ON. PIN required. 2. Press "Cancel" to keep External Transport Mode OFF.
Turn Transport Mode OFF | - Confirm External Transport Mode is OFF | 1. Press "Confirm" to turn External Transport Mode OFF. PIN required. 2. Press "Cancel" to turn External Transport Mode ON.
Cassette present while switching to or from External Transport Mode | - Cassette in Console while switching to or from External Transport Mode | 1. Press "Eject" to remove the Cassette and switch to or from External Transport Mode. See Section 8.2.1 2. Press "Cancel" to discontinue.
Cannot dose while switching to or from External Transport Mode | - Dosing while switching to or from External Transport Mode | 1. Press "Accept." 2. Complete Dosing. 3. Set Dose to 0. 4. Once completed, see Section 8.2.1to enable External Transport Mode or see Section 8.2.9to disable External Transport Mode.

10.7 GaussAlert™ Alarm

The gauss alarm will sound if the GENOSYL DS is too close to the MR Scanner. If the gauss alarm sounds, move the GENOSYL DS away from the MR scanner until the gauss alarm stops sounding.

WARNING

ALWAYS move System away from the MR scanner if the gauss alarm sounds. The gauss alarm will sound if the System is too close to the MR scanner. Move System away from the MR scanner until the gauss alarm stops sounding.

10.8 Troubleshooting

The table below provides resolutions to issues that may be encountered with the GENOSYL DS.

Issue/Symptom | Possible Cause | Recommend Action
Screen does not turn on | - Battery discharged and not connected to AC power - Screen malfunction | 1. Ensure power is properly connected in the back of the unit and the wall outlet. Green light on power supply should be on. 2. Ensure battery is connected properly. 3. Wait for System to charge. 4. Power on System. 5. If not resolved, switch to Back-up Console and contact Technical Support.
Cassette does not insert properly within Console | - Drop or other physical damage | 1. Discard damaged NO Cassette and replace with new Cassette. 2. If new Cassette does not insert properly, switch to Back-up Console and contact Technical Support.
Cassette State Window is not blue | - Drop or other physical damage - Cassette was previously activated | 1. Discard damaged Cassette and replace with new Cassette.
Pumps are louder than normal | - Enclosure damage - Pump malfunction | 1. Contact Technical Support.
Cannot set dose in Primary Dosing Mode | - Flow not detected through Adaptive Sensor - Water Trap/ Sample Line Leak Test was not performed - Calibration is required for at least one sensor | 1. Verify flow is present in patient circuit. 2. Perform Water Trap/ Sample Line Leak Test if not already performed. 3. Perform calibration if required. 4. If issue is not resolved, contact Technical Support.
Console does not shutdown | - Operating System issue or file corruption | 1. Hold the Silver power button on the front down for approximately 10 seconds. The Console should shutdown. 2. If the above does not work, power the Console off with the switch on the back. 3. Contact Technical Support if the issue remains.
Audible alarm tone does not sound after boot-up process | - Speaker hardware failure | 1. Contact Technical Support.
Failed Water Trap / Sample Line Leak Test | - Incorrectly connected the Sample Line to the CAL Port - Test timed out at 60 seconds - Sample line valve not closed properly - Loose gas lines connections - Water Trap not sealed completely - Water Trap seal leak | 1. Ensure proper line connections. 2. Conduct test within 60 seconds. 3. Move the blue stopcock to the closed position. 4. Check Water Trap seal. 5. Replace Water Trap. 6. If issue is not resolved, contact Technical Support
Cassette does not automatically eject from Console | - Mechanism malfunction | 1. Open Cassette Access Door. Simultaneously push the tabs above and below the Cassette to manually eject the Cassette.
Screen Unresponsive | - Screen is frozen | 1. Switch to Back-up Console. 2. Hold Silver Power Button for 10 seconds. 3. Wait for Console to shut down. 4. Switch off and on black rocker switch. 5. Reboot Console.
Adaptive Sensor Not Detected | - Adaptive Sensor Cable Not Connected - Adaptive Sensor not Connected to Adaptive Sensor Cable | 1. Verify Adaptive Sensor Cable is properly plugged into front of Console and the cable is fully inserted. 2. Detach the Adaptive Sensor from the Adaptive Sensor Cable. 3. Wait at least five seconds. 4. Reattach the Adaptive Sensor to the Adaptive Sensor Cable.
Flow Not Detected | - Respiratory Device not delivering flow into circuit - Adaptive Sensor not present in circuit | 1. Ensure Respiratory Device is delivering flow into circuit. 2. Verify Adaptive Sensor is connected in the circuit.
Adaptive Sensor Icon is Yellow | - Adaptive Sensor is not properly connected or has become disconnected - Adaptive Sensor is malfunctioning | 1. Detach the Adaptive Sensor from the Adaptive Sensor Cable. 2. Unplug the Adaptive Sensor Cable from the Console. 3. Wait at least five seconds and reinsert the Adaptive Sensor Cable into the Console. 4. Reattach the Adaptive Sensor to the Adaptive Sensor Cable. 5. If problem persists, replace the Adaptive Sensor. 6. If problem still persists, contact Technical Support.
Higher than desired NO2levels in respiratory circuit | - Low or no flow in patient respiratory circuit - Ventilator flow changed abruptly - Bias flow on respiratory device is too low | 1. Verify flow is present in the patient's respiratory circuit. 2. Allow time for the sensor measurement to adjust while completing the next steps. 3. Verify GENOSYL DS gas line connections are tight by loosening then retightening each connection on the red injection and blue sample lines. 4. If the sensor measurement does not adjust, switch to Back-up Console. 5. Contact Technical Support.
Leak Detection | - Gas lines are not connected properly in the respiratory circuit. - Leak in respiratory circuit - Additional flow in the respiratory circuit. | 1. Verify GENOSYL DS gas line connections are tight by loosening then retightening each connection on the red injection and blue sample lines. 2. Check the respiratory circuit for the presence of leaks. 3. Remove additional flow from respiratory circuit. 4. If problem still persists, contact Technical Support.

10.9 Leak Detection Tool

The GENOSYL DS features a leak detection tool to inform the user that there may be a suspected leak in the GENOSYL DS circuit. The information will be displayed on the "Alarms" tab as pictured in Figure 35. This feature is only available when an Adaptive Sensor is connected in the GENOSYL DS circuit. A leak is suspected if there is a difference between the flow measured by the Adaptive Sensor and estimated flow of the GENOSYL DS injection algorithm. This feature is a diagnostic tool only and the device is properly functioning and delivering NO, even when a leak is detected. However, a leak may result in a decreased Cassette life and should be addressed to ensure optimum Cassette life performance. Refer to Section 10.8Troubleshooting for recommended actions to address a suspected leak.

GENOSYL®DS

SECTION 11
SYSTEM MAINTENANCE

11. SYSTEM MAINTENANCE

11.1 Calibration

This section describes the process for performing high and low calibration for NO, NO2,and O2. Calibration of the GENOSYL DS should be performed every 28 days to ensure the accuracy of NO, NO2, and O2measurements. All calibrations can be performed at any time the Console is powered on, including while actively dosing. Air calibrates the low range for the NO and NO2sensors. The high range of the NO and NO2sensors are calibrated by using calibration gas tanks. The software will notify the user when calibration is due.

The display within the "Calibration" tab provides the status and the calibration due date of the different types of sensors. Air calibration provides the time of the last calibration since the System automatically performs this calibration every 4 hours while actively dosing or every 24 hours while powered on. A green check under status indicates that sensor has successfully been executed within the calibration period. A red X under status indicates that the sensor has not successfully been executed within the calibration period.

During calibration, the display will provide measured readings from each sensor. Note, there are two redundant NO sensors which are used to verify and ensure accuracy of the dosage provided by the System. During calibration, the display will provide a real-time status of the test with colored boxes to the right of the displayed sensor output. A yellow box indicates that the sensor is being calibrated. A green box indicates that calibration was successful for that sensor. A red box indicates that calibration for that sensor failed.

WARNING

- ONLY use the calibration gas pressure regulators supplied by the manufacturer. Pressure regulators not supplied by the manufacturer may damage the sensors and may lead to patient injury.
- ALWAYS verify the correct NIST traceable calibration gas is being used and confirm the expiration date of the calibration gas prior to performing calibration. The use of incorrect or expired gas may result in inaccurate sensor readings and can lead to patient injury.
- NEVER perform NO or NO2calibration within the MR scanner room. Calibration equipment is a potential projectile hazard.

CAUTION

- ALWAYS perform a full-scale calibration of the GENOSYL DS when prompted by the System prior to use.
- ALWAYS confirm the correct flow direction of the installed one-way check valve in the sampling tee to avoid over pressurization of the sample system and damage to the device.

11.1.1 Air Calibration

DISPLAY | ACTION | Warnings, Cautions and Notes
 | 1. Checkto make sure nothing is connected to the CAL port during Air Calibration. 2. If the "Calibration" tab is not displayed, pressthe "Menu" tab to access the sub-level tabs. 3. Pressthe "Calibration" tab on the display menu. 4. Pressthe Low Range "Air" button. 5. Pressthe blue "Start Calibration" button. | NOTE
 | 1. Checkto make sure nothing is connected to the CAL port during Air Calibration. 2. If the "Calibration" tab is not displayed, pressthe "Menu" tab to access the sub-level tabs. 3. Pressthe "Calibration" tab on the display menu. 4. Pressthe Low Range "Air" button. 5. Pressthe blue "Start Calibration" button. | Air Calibration will take up to 2 minutes if not dosing, or 5 minutes if actively dosing. A progress bar is displayed in the lower left-hand corner of the display screen during the calibration process.
 | 1. Press"OK" to continue once calibration is complete. | NOTE
 | 1. Press"OK" to continue once calibration is complete. | If air calibration fails, ensure that nothing is connected to or blocking the CAL port.

11.1.2 NO Calibration

DISPLAY | ACTION | Warnings, Cautions and Notes
 | 1. If the "Calibration" tab is not displayed, pressthe "Menu" tab to access the sub-level tabs. 2. Pressthe "Calibration" tab on the display menu. 3. Pressthe High Range "NO" button. 4. Pressthe gray "Start Calibration" button.
 | 1. Followthe onscreen instructions. | WARNING
 | 1. Followthe onscreen instructions. | DO NOT open the valve prior to connecting to the CAL port. Opening the valve first will expose the user to NO gas. DO NOT interrupt calibration until finished. If interrupted, the calibration will be cancelled.
 | 1. Followthe onscreen instructions. | NOTE
 | 1. Followthe onscreen instructions. | NO calibration takes approximately 2 minutes if not dosing, or 5 minutes if actively dosing. A progress bar is displayed in the lower left-hand corner of the display screen during the calibration process.
 | 1. Followthe onscreen instructions 2. Press"Accept" to continue once calibration is complete. | WARNING
 | 1. Followthe onscreen instructions 2. Press"Accept" to continue once calibration is complete. | DO NOT disconnect tubing from the calibration port prior to closing the valve. Disconnecting the tubing first will expose the user to NO gas.

11.1.3 NO2Calibration

DISPLAY | ACTION | Warnings, Cautions and Notes
 | 1. If the "Calibration" tab is not displayed, pressthe "Menu" tab to access the sub-level tabs. 2. Pressthe "Calibration" tab on the display menu. 3. Pressthe High Range "NO2" button. 4. Pressthe gray "Start Calibration" button.
 | 1. Followthe onscreen instructions. | WARNING
 | 1. Followthe onscreen instructions. | DO NOT open the valve prior to connecting to the CAL port. Opening the valve first will expose the user to NO2gas. DO NOT interrupt calibration until finished. If interrupted, the calibration will be cancelled.
 | 1. Followthe onscreen instructions. | NOTE
 | 1. Followthe onscreen instructions. | NO2calibration takes approximately 2.5 minutes. A progress bar is displayed in the lower left-hand corner of the display screen during the calibration process.
 | 1. Followthe onscreen instructions. 2. Press"OK" once calibration is complete. | WARNING
 | 1. Followthe onscreen instructions. 2. Press"OK" once calibration is complete. | DO NOT disconnect tubing from the calibration port prior to closing the valve. Disconnecting the tubing first will expose the user to NO2gas.

11.2 Maintenance Schedule

The Console components require the following maintenance:

COMPONENT | SCHEDULE
Water Trap | Per patient or as required (per Water Trap/ Sample Line Leak Test)
GaussAlert™ | Monthly functionality check
Console | Every 24 months or 10,000 pump hours, whichever is first

The Console requires factory service every 24 months or 10,000 pump hours, whichever is first. The System will display an Information Message to remind the operator when service is required. Contact Technical Support at 877-337-4118for support or to schedule service.

11.3 Testing the GaussAlert™ Function

WARNING

- Keep the test magnet tool away from pacemakers, ICDs, and other implanted medical devices.
- If either GaussAlert™ fails testing (does not alarm when the magnet tool is used), contact Technical Support at 877-337-4118to request a replacement.
- Do not use the GENOSYL DS in the MR Environment if neither GaussAlert™ is functional.

CAUTION

- Do not use or store the test magnet tool in the MR scanner room.
- Keep the test magnet tool away from the GENOSYL DS user screen. Neodymium magnets can damage computer monitors, watches, pulse oximeters, and other mobile handheld devices.
- Keep the test magnet tool away from magnetic media such as credit cards, magnetic I.D. cards, cassette tapes, video tapes, or other such devices.

NOTE

If the LED stay illuminated for longer than a brief flash, or does not illuminate at all, the battery needs to be replaced. Contact Technical Support at 877-337-4118to request a replacement.

To use the GaussAlert™ test magnet tool to test alarm function, follow the steps listed below.

1. Place the test magnet tool on the GaussAlert™ alarm bracket in the area identified in Figure 36.
2. The alarm will activate and a short flash (less than two seconds) of the LED indicates proper function.
3. Move the test magnet tool away from the GaussAlert™ until the alarm stops sounding.
4. Repeat this procedure on the second GaussAlert™.

11.4 Water Trap Maintenance

The following section will describe the emptying of the Water Trap. The Water Trap should be emptied when the liquid contents reach the horizontal black line marked on the Water Trap.

Prior to emptying the Water Trap, ensure the Gas Sample Line is removed and reattached after emptying the Water Trap.

11.4.1 Emptying the Water Trap

WARNING

ALWAYS empty Water Trap before each use, when prompted by the System, and when the trap is more than half full. Allowing the Water Trap to completely fill will occlude the Sample Line which will interrupt patient gas NO, NO2, and O2concentration monitoring. Failure to monitor the patient gas NO, NO2, and O2concentrations may result in patient injury.

DISPLAY

ACTION

1. RemoveWater Trap from Console by lifting latch and pulling the base of the Water Trap away from the Console.
2. Removethe lid by pulling the lid from the base.
3. Emptythe liquid contents.

1. Reattachthe lid by pushing it back onto base.
2. Slidethe Water Trap back on the Console until it clicks into place.

11.4.2 Water Trap Replacement

If the Water Trap / Sample Line Leak Test fails, and Sample Gas Line integrity is confirmed with blue stopcock in place, replace the Water Trap.

WARNING

- ALWAYS use a Water Trap supplied by the manufacturer. Using an incorrect water trap could result in non-functioning or inaccurate sensor readings.
- ALWAYS conduct Water Trap/ Sample Line Leak Test every time you empty or replace the Water Trap, as failure to do so may lead to an incorrect NO reading, which can result in injury or death.

DISPLAY

ACTION

1. Removeold Water Trap from Console by lifting the latch and pulling the base of the Water Trap away from the Console.

1. Slidenew Water Trap back on the Console until it clicks into place. Replace sample line to Water Trap.
2. Discardthe old Water Trap.

11.5 Battery

The battery will be serviced during scheduled maintenance performed by the manufacturer. If the need arises to replace the battery sooner than scheduled contact Technical Support at 877-337-4118to schedule a maintenance appointment. Battery is expected to last up to four hours under optimal conditions. Console will alarm when less than 15 minutes of battery life remains. See Section 10.3if you receive a Battery Error.

During storage, the GENOSYL DS may be stored with the power off, but the external power supply should be connected at least once every 3 months to ensure a minimum charge is maintained on the internal battery (see Section 13.6for additional information).

WARNING

ONLY properly trained personnel should replace the battery. Incorrectly replacing the battery may result in a hazard such as excessive temperatures, fire, or explosion.

11.6 Cleaning

11.6.1 Enclosure, Connections, and Surfaces Other Than the Display

Prior to performing any cleaning or maintenance operations ensure that the GENOSYL DS Console has been completely powered down as specified in Section 6.1and that the AC/DC power supply external to the GENOSYL DS Console has been unplugged. Apply any mild detergent to cloth prior to wiping the System. Gently clean the outer surface of the Console, Cart, and Adaptive Sensor Cable with a soft damp cloth and mild detergent or isopropyl alcohol (70%).

CAUTION

- DO NOT sterilize (e.g., autoclave, gas sterilize) any of the components of the System, as this may compromise performance.
- DO NOT use harsh cleaning agents (see Table 11) on the GENOSYL DS. Doing so may impair the structural integrity and/or function of the device.
- ONLY use a damp cloth to clean the Console and limit use of liquids around Console. Excess water can permanently damage the device.
- ALWAYS ensure the System is completely dry after cleaning before powering it ON. Failure to do so could result in equipment damage.

WARNING

- NEVER submerge the GENOSYL DS, Cassette, or non-disposable Adaptive Sensor Cable. Submerging in liquid will damage the System and could cause electrical shorts which may result in injury or death.
- DO NOT clean the GENOSYL DS with the power connected and the System turned ON, as this may lead to injury (e.g., shock). Unplug AC/DC power supply external to the System prior to cleaning.

Table 11: Recommended Cleaning Agents
CLEANING AGENT | ACTIVE INGREDIENTS
Avert by Diversey | Sodium hypochlorite 1.312% Other ingredients 98.688%
Oxivir by Diversey | Hydrogen Peroxide 0.5% Other ingredients 99.5%
CaviWipesXL by Metrex | Disobutylphenoxyethxyethyl dimethyl benzyl ammonium chloride 0.28% Isopropanol 17.20% Inert ingredients 82.52%
Sani-Cloth AF3 by PDI Healthcare | n -Alkyl dimethyl ethybenzyl ammonium chlorides 0.14% n-Alkyl dimethyl benzyl ammonium chlorides 0.14% Other ingredients 99.72%
Super Sani-cloth by PDI Healthcare | n -Alkyl dimethyl ethybenzyl ammonium chlorides 0.25% n-Alkyl dimethyl benzyl ammonium chlorides 0.25% Isopropyl Alcohol 55.00% Other ingredients 44.50%

11.6.2 Display Screen

Turn off Console and disconnect from AC power. Gently clean with a damp cloth.

CAUTION

- DO NOT touch or rub the display screen with abrasive cleaning compounds or organic solvents, as they may scratch and damage the screen.
- DO NOT spray or pour liquids directly on the controller or the display, as they may damage the screen.

11.6.3 Cleaning the Gauss Alarms Mount

Use a soft cloth dampened with water to clean the enclosure. Use an aqueous solution of up to 75% isopropyl alcohol for more efficient cleaning. Disinfection may be accomplished with the use of denatured alcohol.

11.7 Storage

11.7.1 Cart / Console Storage

The acceptable storage conditions for the Cart/Console are shown in the following table.

 | Temperature | -20⁰ C to 60⁰ C
Cart / Console Storage | Humidity | 15% to 95%, non-condensing
 | Pressure | 57 kPa to 110 kPa

During storage, the GENOSYL DS may be stored with the power off, but the external power supply should be connected at least once every 3 months to ensure a minimum charge is maintained on the internal battery (see Section 13.6for additional information).

WARNING

- MAKE SURE the GENOSYL DS is connected to AC wall power to charge the battery a minimum of once every 3 months to maintain a minimum battery charge. Failure to recharge the Console battery for extended timeframes may result in full discharge of the battery. If a Battery Error message occurs during startup of the System, contact Technical Support at 877-337-4118for assistance.
- ONLY properly trained personnel should replace the battery. Incorrectly replacing the battery may result in a hazard such as excessive temperatures, fire, or explosion.
- ONLY store the GENOSYL DS as outlined in the storage instructions. Not storing the device in alignment with its storage instructions can cause the device to be unsafe and lead to injury or death.

11.7.2 Cassette / Accessory Storage

GENOSYL DS may not function correctly if the Cassette or any of the System Accessories have been exposed to high levels of heat or humidity. Cassettes are supplied in a plastic container and should remain unopened until use. Cassettes should be stored at 25°C (77°F) with excursions permitted between 15°C to 30°C (59°F to 86°F). (See USP Controlled Room Temperature).

GENOSYL®DS

SECTION 12
MECHANICAL VENTILATION

12. MECHANICAL VENTILATION

WARNING

- ONLY mechanical ventilators validated with the GENOSYL DS should be used. Not using a validated ventilator system can result in injury or harm.
- DO NOT use the GENOSYL DS with circle anesthesia ventilator systems. The GENOSYL DS has not been characterized or qualified for use with anesthesia breathing systems with recirculation of gases.

12.1 Mechanical Ventilation

There are two main effects of connecting the GENOSYL DS to a ventilator breathing circuit:

- The System injects up to 0.9 LPM of NO/air (21% Oxygen) into the inspiratory output of the ventilator.
- The System samples up to 0.3LPM from the ventilator circuit as a measurement to the built-in gas analyzers

The results of adding and subtracting gas into the ventilator circuit are described in sections 12.1.1 to 12.1.4:

12.1.1 Oxygen Dilution

The ventilator typically is flowing gas to the patient with enhanced oxygen content from room air, ranging from 21% at 100% oxygen. The DS is injecting NO mixed with air with a concentration of oxygen at nominally 21%. Thus, except for the case where the ventilator is supplying gas to the patient at 21% oxygen, there is some dilution of the oxygen delivered to the patient.

This dilution may be determined with the following equation:

Percent O2to Patient = [{%O2/100 + (Flowinj/Flowvent)×0.21}/{1 + (Flowinj/Flowvent)}]×100

Where:

1. Flowinj= Injection flow in same units as ventilator flow
2. Flowvent= Ventilator flow in same units as injection flow
3. %O2= Percent oxygen out of ventilator
4. 0.21 = Fraction of oxygen in injection flow (21%)

Table 12below shows the maximal dilution effect on the concentration of oxygen supplied to the patient for set ventilator flow settings with NO doses ≤40 ppm and a nominal flow from the GENOSYL DS of 0.6 LPM of NO/air (21% oxygen) into the inspiratory output of the ventilator. Actual dilution may vary based on respiratory device settings and clinical scenarios.

This is applicable for all compatible gas delivery systems, unless otherwise noted below.

NOTE

The following respiratory devices demonstrated oxygen dilution that is representative of in ection flow greater than 0.6LPM in testing with NO doses ≤ 40 ppm. Use the calculation above to estimate maximal dilution using Flowinj = 0.64 LPM:

- Bio-Med Devices MVP-10

Table 12: Oxygen Dilution
 | Oxygen (%) Supplied from Ventilator
 | 100 | 80 | 60 | 40 | 21
Ventilator Flow (LPM) | Oxygen (%) Delivered to Patient
70 | 99 | 79 | 60 | 40 | 21
20 | 98 | 78 | 59 | 39 | 21
15 | 97 | 78 | 59 | 39 | 21
10 | 96 | 77 | 58 | 39 | 21
9 | 95 | 76 | 58 | 39 | 21
8 | 94 | 76 | 57 | 39 | 21
7 | 94 | 75 | 57 | 39 | 21
6 | 93 | 75 | 56 | 38 | 21
5 | 92 | 74 | 56 | 38 | 21
4 | 90 | 72 | 55 | 38 | 21
3 | 87 | 70 | 54 | 37 | 21
2 | 82 | 66 | 51 | 36 | 21
1 | 70 | 58 | 45 | 33 | 21
0.5 | 57 | 48 | 39 | 30 | 21

Higher injection flows may be employed by the GENOSYL DS when administering NO doses >40 ppm. Use injection flow of 0.9 LPM to estimate the maximal dilution effect on the concentration of oxygen supplied to the patient when administering NO doses >40 ppm.

12.1.2 Minute Volume

When using volume ventilation with the GENOSYL DS, the tidal volume delivered to the patient may show small changes due to the addition and subtraction of gases by the Delivery System. Some minor ventilator adjustments to the minute volume may be required. Maximum total flow added to the ventilator circuit is 0.9 LPM of concentrated NO gas and the maximum total flow removed from the ventilator circuit is 0.3 LPM of sampled gas.

12.1.3 Trigger Sensitivity

The addition and subtraction of gases by the GENOSYL DS may affect the trigger sensitivity of the ventilator when using synchronized modes of ventilation. This may cause ventilators which have flow trigger modes to auto-cycle or result in apnea alarms, especially where the trigger flow is less than the total flow added.

12.1.4 Maximum NO Delivery

The maximum combination of dose (ppm) and flow (LPM) is 800 ppm × LPM (e.g., 20 ppm with 40 LPM, 40 ppm at 20 LPM, etc.). The System is capable of delivering NO at a minimum of 1 ppm × LPM (e.g., 1 ppm at 1 LPM). See the graph below for the minimum and maximum dose ranges for the System, based on ventilator circuit total minute volume.

12.1.5 Bias Flow and NO2

The GENOSYL DS has a safety fallback where the delivery of nitric oxide will be interrupted when a sampled value higher than 3 ppm NO2is detected. Once sample value of NO2is below 3.0 ppm, the Console will auto resume delivery of NO at set dose. The table below outlines the dose at which a delivery interruption was observed during validation testing in a laboratory setting due to high NO2. For validation testing, FiO2was set at 100% and the maximum bias flow setting for each ventilation device was used. If there is an unexpected change in NO2concentration, the delivery system should be assessed in accordance with the recommended actions for troubleshooting Section 10.8, and the NO2analyzer should be recalibrated. The dose of GENOSYL and/or FiO2should be adjusted as appropriate.

CAUTION

- When using spontaneousbreathing modes on respiratory device, NO2levels may exceed 3.0 ppm when dosing ≥ 57 ppm NO into 100% FiO2and maximum bias flow, resulting in nitric oxide delivery interruption. Once sample value of NO2is below 3.0 ppm, the Console will auto resume delivery of NO at set dose. Refer to Section 12.1.5 Table 13for additional information.
- When using non-spontaneousbreathing modes on respiratory device, NO2levels may exceed 3.0 ppm when dosing ≥ 63 ppm NO into 100% FiO2and maximum bias flow, resulting in nitric oxide delivery interruption. Once sample value of NO2is below 3.0 ppm, the Console will auto resume delivery of NO at set dose. Refer to Section 12.1.5 Table 13for additional information.

Table 13: NO Dose at which NO2exceeded 3ppm NO2Threshold when dosing at 100% FiO2and Maximum bias flow
Manufacturer | Model | Set NO dose at which NO2exceeded 3 ppm threshold in spontaneous modes | Set NO dose at which NO2exceeded 3 ppm threshold in nonspontaneous modes
Bio-Med Devices | Crossvent 2+ | 64 | 82
Bio-Med Devices | MVP-10 | 75 | 70
Drӓger | V500, VN 500, V600, VN 600, V800, VN 800 | 69 | 72
Hamilton | C1/MR1/T1 | 72 | 70
Hamilton | C6 | 72 | 67
Hamilton | G5 | 72 | N/A
Puritan Bennett | 980 | 59 | 64
Vyaire Medical Inc. | AVEA | 74 | 82
Fisher & Paykel | Optiflow JR 2 | 57 | N/A
Fisher & Paykel | Optiflow | 69 | N/A

12.2 Ventilator Compatibility

VERO Biotech performs validation testing which determines the compatibility of ventilator/gas delivery systems with the GENOSYL DS. During this compatibility testing, the GENOSYL DS is evaluated for the following parameters while connected to each ventilator/gas delivery system:

- NO Dose Accuracy:Continuous and accurate delivery of a targeted dose of nitric oxide within ± 20% of setpoint or within ± 2 ppm, whichever is greater.
- Respiratory Device Breath Delivery and Alarms:The respiratory device breath delivery and alarms continue to function as intended by the manufacturer across the range of operating conditions.
- NO2Performance: NO2remains within acceptable limits less than 1.0 ppm with 60% FiO2and ≤40 ppm NO.
- O2Dilution: Post dilution O2level delivery is maintained within acceptable limits and conforms with the information presented in the GENOSYL DS Operator's Manual, Section 12.1.1, "Oxygen Dilution".
- NO Concentration Transients:NO concentration transients are ≤150% of mean concentration and as low as 0.0 ppm as long as the transient duration does not exceed 10% of the volumetric duration of the breath.

The testing performed demonstrated conformance with all specified requirements. The following ventilators and non-invasive gas delivery systems in Table 14have been validated for use with the GENOSYL DS. See Section 3.2for use configurations.

WARNING

- ALWAYS use the GENOSYL DS in accordance with the indications, usage, contraindications, warnings, and precautions described in the GENOSYL prescribing information and labeling. Refer to latest approved prescribing information and labeling prior to use.
- The approved patient population for the GENOSYL DS as specified in the drug labeling for GENOSYL (nitric oxide) for inhalation, is limited to neonates. The GENOSYL DS is not intended to be used in other patient populations.

Table 14: Details of Validated Systems

Validated ventilators were not tested with a nebulizer.

Use of a Mixer is recommended when delivering in specific tidal volume ranges on various ventilation devices. Refer to Table 15for when a Mixer is and is not recommended.

Manufacturer | Models | Hospital | External Transport | Anesthesia Gas Machine | Modes Validated
Bio-Med Devices | Crossvent 2+ | • | • |  | • Cycle • CPAP
Bio-Med Devices | MVP-10 | • | • |  | • Cycle • CPAP
Dräger | Fabius GS, Fabius GS Premium, Fabius Tiro |  |  | • | • VC • PC • PS • SIMV/PS
Dräger | V500, VN 500, V600, VN 600, V800, VN800 | • |  |  | • VC-AC • VC-SIMV • VC-CMV • PC-AC • PC-SIMV • PC-CMV • PC-BIPAP • VC-MMV • PC-APRV • PC-PSV • SPN-CPAP/PS • SPN-CPAP/VS • SPN-PPS
GE | Aisys CS2 |  |  | • | • VCV • PCV • PCV-VG • PSVPro • CPAP+PSV • SIMV PCV • SIMV VCV • SIMV PCV-VG • Manual
Hamilton | C1/MR1 | • |  |  | • PCV+ • PSIMV+ • APVcmv • APVsimv/SIMV+ • ASV • DuoPAP • APRV • SPONT • NIV • NIV ST • nCPAPA • nCPAP PC
Hamilton | C6 | • |  |  | • APVcmv • APVsimv • PCV+ • PSIMV+ • DuoPAP • APRV • SPONT • ASV • NIV • NIV-ST • nCPAP-PS
Hamilton | G5 | • |  |  | • (S)CMV • P-CMV • P-SIMV • APVcmv • APVsimv • ASV • DuoPAP • APRV • SPONT • VS • NIV • NIV-ST • nCPAP-PS • SIMV
Hamilton | T1 | • | • |  | • PCV+ • PSIMV+ • APVcmv • APVsimv/SIMV+ • ASV • DuoPAP • APRV • SPONT • NIV • NIV ST • nCPAP • nCPAP PC
Puritan Bennett | 980 | • |  |  | • A/C PC • A/C VC • A/C VC+ • NIV AC PC • NIV AC VC • BiLevel • BiLevel PC PS • BiLevel PC TC • NIV CPAP • SPONT VS • NIV SPONT PS • SPONT TC • SPONT PAV+
Vyaire Medical Inc. | AVEA | • |  |  | • Volume A/C • Pressure A/C • Volume SIMV • Pressure SIMV • CPAP/PSV • PRVC A/C • PRVC SIMV • APRV/BiPhasic • TCPL A/C • TCPL SIMV • Nasal CPAP/IMV
Fisher & Paykel | Optiflow JR 2 | • |  |  | • N/A
Fisher & Paykel | Optiflow | • |  |  | • N/A

Table 15: Validated Compatibility with and without Inline Mixer

At the lowest tested rate of 6 BPM, a Mixer may be used to reduce intra-breath dose variability as outlined in Table 15 below. Intra-breath dose variability was not observed at a respiratory rate of 60 BPM.

For mixer recommendations when using an anesthesia gas machine, refer to Table 6.

See Section 3.4for assembly instructions for Injection Assembly with Adaptive Sensor and Mixer Assembly with Adaptive Sensor.

GENOSYL®DS

SECTION 13
PRODUCT SPECIFICATIONS

13 PRODUCT SPECIFICATIONS

13.1 System Performance

NO DOSING
Accuracy | ± 20% or ± 2 ppm (whichever is greater)
Range | 0 to 80 ppm
Flow rate (max) | 900 mL/min

GAS SENSOR
 | Range | Resolution | Accuracy
NO | 0 - 10 ppm | 0.1 ppm | ≤20 ppm: ± (20% of actual concentration + 0.5) >20 ppm:± (10% of actual concentration + 0.5)
NO | 10 – 100 ppm | 1 ppm | ≤20 ppm: ± (20% of actual concentration + 0.5) >20 ppm:± (10% of actual concentration + 0.5)
NO2 | 0.0 - 12 ppm | 0.1 ppm | ± 20% of actual concentration, or ± 0.5 ppm, whichever is greater
O2 | 18 - 100% | 1% | ± volume fraction of 2.5% +2.5% of gas level

13.2 System Classification

- Class I equipment
- Ordinary Equipment IPX1
- Continuous Use
- Essential Performance: The System shall continue to deliver a controlled dose, as configured by the user (e.g., 20 ppm @ 6 LPM within +/- 20%) with NO2< 3 ppm and O2= 21 ±3% in room air for the specified range of use conditions.

13.3 Testing

- ANSI ES 60601-1
- IEC 60601-1-2
- IEC 60601-1-8

13.4 Electrical

NOTE

Disconnect main power cord from the wall outlet to isolate equipment from main power. Do not position equipment to make it difficult to disconnect equipment from main power.

13.5 Power Supply

- Medical Grade Class I
- Input: 100-240 V, 50-60 Hz, 2A
- Output: 18 V DC, 8.3 A
- 150 Watts Max

13.6 Battery

- Fully charged Battery is expected to last up to four hours under optimal conditions. Console will alarm when less than 15 minutes of battery life remains. See Section 10.3if you receive a Battery Error.
- Typical battery life is 300 charge/discharge cycles.
- The battery will be serviced during scheduled maintenance performed by the manufacturer.
- If the need arises to replace or dispose of the battery sooner than scheduled contact Technical Support to schedule a maintenance appointment.

The battery has an embedded 5 segment LCD battery indicator viewable through side panel window. The segments will display the following information:

- 5 segments filled – 81%-100% charged
- 4 segments filled – 61%-80% charged
- 3 segments filled – 41%-60% charged
- 2 segments filled – 21%-50% charged
- 1 segment filled – 1% - 20% charged
- No battery indication – below 1%
- Most significant segment flashing – charging
- Most significant segment not flashing – not charging

13.6.1 Battery Charge Status Indicator

COLOR | ERROR
Solid Red | Battery Power Supply Error
Blinking Red | Communication Failure or Hardware Error
Solid Amber | Console is unplugged and using battery power
Blinking Amber | Console is running and running on low battery
Solid Green | Console is plugged in and battery is fully charged
Blinking Green | Console is plugged in and the battery is charging

13.17 Display

- Touch screen – Resistive
- Brightness – 400 cd/m^2
- Resolution – 800 × 480 pixels, color

13.8 Mechanical

CART
Weight | 18.15 kg (40.01lbs)
Width × Length | 47.8 cm (18.8 in) × 66.7 cm (26.3 in)
Height | 120.7 cm (47.5 in)

CONSOLE
Weight | 8.85 kg (19.75 lb)
Width × Length | 40.6 cm × 30.5 cm (16 in × 12 in)
Height | 17 cm (6.75 in)

CASSETTE
Weight | 0.42 kg (0.93 lb)
Width × Length | 11.4 × 3.8 cm (4.5 in × 1.5 in)
Height | 13 cm (5.1in)

13.9 Environmental

ENVIRONMENTAL RANGES
Operating | Temperature | 5⁰ C to 40⁰ C
Operating | Humidity | 15% to 95%, non-condensing
Operating | Pressure | 57 kPa to 110 kPa
Operating | Altitude | Under 15,000 feet
Storage | Temperature | -20⁰ C to 60⁰ C
Storage | Humidity | 15% to 95%, non-condensing
Storage | Pressure | 57 kPa to 110 kPa
Storage | Altitude | Under 15,000 feet
Water Ingress Protection | IPX1

13.10 GaussAlert™ Specifications

Standard Factory Preset Alarm Thresholds | 100 Gauss (10 mT)
Audio Alarm Typical Sound Pressure | 92dB (A) at 24 inches
Audio Alarm Frequency | 2900 Hz +/- 250Hz
Typical Battery Life | 5 years
Sensor Type | Mechanical with panoramic uniform sensitivity

13.11 MR Signal-to-Noise Ratio and Artifact Dimension Analysis

MR image artifact was evaluated using 1.5 T and 3 T MRI Systems. Testing was conducted using standard American College of Radiology (ACR) sequences and a standard ACR large phantom placed inside a transmit-receive head coil. Duplicate sequences were performed to acquire the same images with and without the GENOSYL DS operating on battery power inside the MRI suite.

The GENOSYL DS compatibility test results are as follows:

Artifact Dimensional Analysis | 1.5 T | The maximum dimensional change in images acquired during the operation of the GENOSYL DS was < 1 mm.
Artifact Dimensional Analysis | 3 T | The maximum dimensional change in images acquired during the operation of the GENOSYL DS was < 1 mm.
Image Quality Signal-to-Noise Ratio Analysis | 1.5 T | The average SNR change was -35%. The average SFNR change was -42%. The PIU values were all 96%.
Image Quality Signal-to-Noise Ratio Analysis | 3 T | The average SNR change was -25%. The average SFNR change was -22%. The PIU values were all greater than 94%.

The GENOSYL DS does not distort the geometric accuracy and the image intensity uniformity is not adversely affected by the presence of the GENOSYL DS at the 100 Gauss line. The SNR and SFNR are both impacted by the presence of the GENOSYL DS, to a more pronounced degree when the equipment is powered via a wall outlet inside the MRI suite versus operating on the battery.

NOTE

- The test results presented here were obtained with the GENOSYL DS operating on battery power.
- If using the GENOSYL DS while connected to wall power, it is recommended to route the power cords through a waveguide.

13.12 EMI/EMC

Emissions test | Compliance | Electromagnetic Environment – Guidance
RF emissions CISPR 11 | Group 1 | The GENOSYL DS uses RF energy only for its internal function. Therefore, its RF emissions are very low and are not likely to cause any interference in nearby electronic equipment.
 | Class B | The GENOSYL DS is suitable for use in all establishments, including domestic establishments and those directly connected to the public low voltage power supply network that supplies buildings used for domestic purposes.
RF conducted emissions per CISPR 11 Ed. 5.1b:2010 | Class B | The GENOSYL DS is suitable for use in all establishments, including domestic establishments and those directly connected to the public low voltage power supply network that supplies buildings used for domestic purposes.
Harmonic emissions IEC 61000-3-2 | Class A | The GENOSYL DS is suitable for use in all establishments, including domestic establishments and those directly connected to the public low voltage power supply network that supplies buildings used for domestic purposes.
Voltage fluctuations/flicker emissions IEC 61000-3-3 | Complies | The GENOSYL DS is suitable for use in all establishments, including domestic establishments and those directly connected to the public low voltage power supply network that supplies buildings used for domestic purposes.

Guidance and Manufacturer's Declaration – Electromagnetic Immunity
The GENOSYL DS is intended for use in the electromagnetic environment specified below. The customer or the user of the GENOSYL DS should assure that it is used in such an environment
Immunity Test | IEC 60601 Test Level | Compliance Level | Electromagnetic Environment - Guidance
Electrostatic discharge (ESD) IEC 61000-4-2 | ±8 kV contact ±15 kV air | ±8 kV contact ±15 kV air | The relative humidity should be at least 5%.
Electrical fast transient/burst IEC 61000-4-4 | ±2 kV for power supply lines | ±2 kV for power supply lines | Mains power quality should be that of a typical commercial or hospital environment.
Surge IEC 61000-4-5 | AC line: Line to Line ±0.5kV, ±1 kV & Line to GND ±0.5kV, ±1 kV, ±2kV | AC line: Line to Line ±0.5kV, ±1 kV & Line to GND ±0.5kV, ±1 kV, ±2kV | Mains power quality should be that of a typical commercial or hospital environment.
Voltage dips, short interruptions and voltage variations on power supply input lines IEC 61000-4-11 | 0% during 0.5 cycle 0% (100% reduction) for 1 cycles 70% (30% reduction) for 25 cycles 0% for 250 cycles- Short interruptions | 0% during 0.5 cycle 0% (100% reduction) for 1 cycles 70% (30% reduction) for 25 cycles 0% for 250 cycles- Short interruptions | Mains power should be that of a typical commercial or hospital environment. If the user of the GENOSYL DS requires continued operation during power mains interruptions, it is recommended that the GENOSYL DS be powered from an uninterruptible power supply or a battery.
Power frequency (50/60 Hz) Magnetic field IEC 61000-4-8 | 30 A/m | 30 A/m with dwell time of 60sec | Power frequency magnetic fields should be at levels characteristic of a typical location in a typical commercial or hospital environment.
NOTE: UTis the AC main voltage prior to application of the test level.
Conducted RF IEC 61000-4-6 | 6 V rms 150 kHz to 80 MHz in ISM bands [The ISM (industrial, scientific and medical) bands between 150 kHz and 80 MHz are 6.765 MHz to 6.795 MHz; 13.553 MHz to 13.567 MHz; 26.957 MHz to 27.283 MHz; and 40.66 MHz to 40.70 MHz.] | 10 V 80% AM @ 1 kHz 150 kHz - 80 MHz in ISM bands, | Except as indicated on page 10-137, portable and mobile RF communications equipment, including cables, should be used no closer to any part of the GENOSYL DS than the recommended separation distance calculated from the equation applicable to the frequency of the transmitter.
 |  |  | Recommended separation distance: d=1.2√P d=1.2√P d=1.2√P 80 MHz to 800 MHz d=2.3√P 800 MHz to 2.7 GHz where P is the maximum output power rating of the transmitter in watts (W) according to the transmitter manufacturer and d is the recommended separation distance in meters (m). [The compliance levels in the ISM frequency bands between 150 kHz and 80 MHz and in the frequency range 80 MHz to 2.7 GHz are intended to decrease the likelihood that a portable communications device could cause interference if it is inadvertently brought into patient areas. For this reason, an additional factor of 10/3 is used in calculating the recommended separation distance for transmitters in these frequency ranges.]
Radiated RF IEC 61000-4-3 | 10 V /m 80MHz to 2.7 GHz | 10 V /m 80 MHz to 2.7 GHz | Recommended separation distance: d=1.2√P d=1.2√P d=1.2√P 80 MHz to 800 MHz d=2.3√P 800 MHz to 2.7 GHz where P is the maximum output power rating of the transmitter in watts (W) according to the transmitter manufacturer and d is the recommended separation distance in meters (m). [The compliance levels in the ISM frequency bands between 150 kHz and 80 MHz and in the frequency range 80 MHz to 2.7 GHz are intended to decrease the likelihood that a portable communications device could cause interference if it is inadvertently brought into patient areas. For this reason, an additional factor of 10/3 is used in calculating the recommended separation distance for transmitters in these frequency ranges.]
 |  |  | Field strengths from fixed RF transmitters, as determined by an electromagnetic site survey, [Field strengths from fixed transmitters, such as base stations for radio (cellular cordless) telephones and land mobile radios, amateur radio, AM and F M radio broadcast and TV broadcast cannot be predicted theoretically with accuracy. To assess the electromagnetic environment due to fixed R transmitters, an electromagnetic site survey should be considered. If the measured field strength in the location in which the GENOSYL DS is used exceeds the applicable RF compliance level above, the GENOSYL DS should be observed to verify normal operation. If abnormal performance is observed, additional measures may be necessary, such as reorienting or relocating the GENOSYL DS.] should be less than the compliance level in each frequency range. [Over the frequency range 150 kHz to 80MHz, field strengths should be less than 3 V/m.] Interference may occur in the vicinity of equipment marked with the following symbol:

NOTE

NOTE 1: At 80 MHz and 800 MHz, the higher frequency range applies.
NOTE 2: These guidelines may not apply in all situations. Electromagnetic propagation is affected by absorption and reflection from structures, objects and people.

Recommended separation distances between portable and mobile RF communications equipment and the GENOSYL DS
The GENOSYL DS is intended for use in an electromagnetic environment in which radiated RF disturbances are controlled. The customer or the user of the GENOSYL DS can help prevent electromagnetic interference by maintaining a minimum distance between portable and mobile RF communications equipment (transmitters) and the GENOSYL DS as recommended below, according to the maximum output power of the communications equipment except as indicated on page 10-166.
Rated Maximum Output Power of Transmitter W | Separation Distance According to Frequency of Transmitter, m
Rated Maximum Output Power of Transmitter W | 150 kHz to 80 MHz d=1.2√P | 80 MHz to 800 MHz d=1.2√P | 800 MHz 2.5 GHz d=2.3√P
0.01 | 0.12 | 0.12 | 0.23
0.1 | 0.38 | 0.38 | 0.73
1 | 1.2 | 1.2 | 2.3
10 | 3.8 | 3.8 | 7.3
100 | 12 | 12 | 23
For transmitters rated at a maximum output not listed above, the recommended separation distance d in meters (m) can be estimated using the equation applicable to the frequency of the transmitter, where P is the maximum output power rating of the transmitter in Watts (W) according to the transmitter manufacturer.

Immunity Test | Standards Tested | Compliance Level | Electromagnetic Environment - Guidance
Radiated RF AIM 7351731 - Medical Electrical Equipment and System Electromagnetic Immunity Test for Exposure to Radio Frequency Identification Readers | - ISO 14223 (Annex A) - ISO/IEC 14443-3 (Type A) (Annex B) - ISO/IEC 14443-4 (Type B) (Annex C) - ISO/IEC 15693 (ISO/IEC 18000-3 Mode 1) (Annex D) - ISO/IEC 18000-7 (Annex E) - ISO/IEC 18000-63 Type C (Annex F) - ISO/IEC 18000-3 (Mode 3) - ISO/IEC 18000-4 Mode 1 (Annex G) | Per the Annex in the standard | System tested as compatible with RFID tags/communication

Frequencies of portable and mobile transmitters for which the recommended separation distance is 30 cm (12 in).

Band (MHz) | Service
380 - 390 | TETRA 400
430 - 470 | GMRS 460, FRS 460
704 - 787 | LTE Band 13, 17
800 - 960 | GSM 800/900 TETRA 800, iDEN 820, CDMA 850, LTE Band 5
1,700 – 1,990 | GSM 1800; CDMA 1900; GSM 1900; DECT; LTE Band 1, 3, 4, 25; UMTS
2,400 – 2,570 | Bluetooth, WLAN, 802.11 b/g/n, RFID 2450, LTE Band 7
5,100 – 5,800 | WLAN 802.11 a/n

GENOSYL®DS

INDEX

KEY WORD INDEX
Adjusting the dose | 113
Adjustments, alarms, high and low levels for NO, NO2, and O2 | 185
Adjustments, date and time | 59
Adjustments, dose in manual mode | 56
Adjustments, dose in primary mode with keypad | 62
Adjustments, ventilator for minute volume | 234
Aerosol Delivery | 95
Alarm, Battery Error | 194
Alarm, Calibration Required | 193
Alarm, Hardware Failure | 193
Alarm, Line Occlusion | 195, 196
Alarm, Low NO | 192
Alarms, Battery Not Detected | 197
Alarms, Cassette Failure | 200
Alarms, Cassette Not Operational | 198
Alarms, Cassette Time Remaining | 201
Alarms, Configuration Parameters Incorrect | 197
Alarms, Delivery Flow Error | 202
Alarms, Gauss alarm | 207
Alarms, High NO2/NO shutdown | 190
Alarms, High O2 | 201
Alarms, Low Battery | 200
Alarms, Low O2 | 201
Alarms, Service Due Date Expired | 201
Alarms, Service Due Date Within 2 Days | 205
Alarms, Service Required | 194, 198
Alarms, System Running on Battery Only | 204
Alarms, Water Trap Not Detected | 196
ANESTHESIA GAS MACHINES | 174
Bagging | 116
Bagging, manual ventilation | 116
Bagging, manual ventilation circuit setup | 74, 93
Battery, backup | 33
Battery, error alarm | 194
Battery, low battery alarm | 200
Battery, not detected alarm | 197
Buttons, operational, display screen | 61
Calibration, Air | 217
Calibration, auto air calibration required | 198
Calibration, calibration due | 206
Calibration, calibration due date | 216
Calibration, calibration due in less than 3 days | 205
Calibration, calibration failed message | 198
Calibration, calibration required alarm | 193
Calibration, explanation | 216
Calibration, history | 59
Calibration, NO | 218
Calibration, NO2 | 220
Calibration, tab | 58
Cart, storage | 228
Cassette, activation | 110
Cassette, cassette status on display screen | 63
Cassette, damage | 208
Cassette, description | 49
Cassette, disposal | 38, 128
Cassette, failure alarm (cassette not operational) | 200
Cassette, indication of use | 49
Cassette, indicator not blue | 208
Cassette, insertion | 101
Cassette, mechanical specifications | 246
Cassette, output range | 234
Cassette, removal | 124, 167
Cassette, storage | 228
Cassette, to expire alarm (time remaining) | 201
Cassette, to expire message (time remaining) | 206
Cassette, Water Trap / Sample Line Leak Test | 68
Cautions | 3, 178
Cautions, User Responsibility | 32
Cleaning, console | 226
Cleaning, display screen | 227
Cleaning, GaussAlert | 227
Components, use of non-specified components | 74
Components, use outside of product labeling | 9
Connections, console | 86
Connections, example ventilator circuit setup | 74
Connections, GENOSYL DS ventilator circuit | 91
Connections, manual ventilation bag | 93
Connections, Non-Invasive Gas Delivery Systems | 79
Connections, power cord to console | 100
Connections, Standard Ventilators | 75
Connections, ventilator circuit | 94
Console, backup battery | 33
Console, cleaning | 226
Console, connections | 86, 87
Console, gas monitoring | 37
Console, maintenance schedule | 222
Console, mechanical specifications | 246
Console, modes operation | 56
Console, primary definition | 19
Console, repair or replacement | 32
Console, standby definition | 19
Console, start up | 100
Console, storage | 228
Console, use as a backup | 120
Console, user responsibility | 32
Date, alarm history | 186
Date, calibration due date | 216
Date, calibration due date passed | 206
Date, change date and time | 59
Date, expiration | 81
Date, manufacture | 21
Date, service date within 2 days | 205
Date, service due within 14 days | 205
Date, service past due | 201
Date, use by | 23
Display, cleaning | 227
Display, definition | 19
Display, menu tab navigation | 57
Display, screen | 56
Display, screen cassette status | 63
Display, screen operational buttons | 61
Display, screen overview | 56
Display, specifications | 246
Dosing, during manual (bagging) ventilation | 116, 164
Dosing, during use as a backup | 120
Dosing, resuming primary dosing | 119, 166
Dosing, system performance specifications | 244
EMI/EMC, specifications | 248
External Transport Transport, External | 138
External Transport Cassette | 142
Feedback loop, explanation | 33
Fresh Gas Flow | 176
Gas lines, detailed explanation | 54
Gas monitoring | 37
Gauss alarm | 207
GaussAlert maintenance | 222, 223
GaussAlert specification | 247
GaussAlert, cleaning | 227
GaussAlert, testing | 223
Height, cart specifications | 246
Height, cassette specifications | 246
Humidity, operating humidity | 247
Humidity, storage/transport | 247
Indications for Use | 33
Injection Assembly | 83
Injection Assembly, assembly | 83, 149
Label, expiration date | 81
Labeling, intended population for use | 33
Labeling, use outside of | 9
Labeling, user responsibility | 32
Lable, gas lines | 54
Maintenance, GaussAlert | 222
Manual ventilation | 116, 164
Manual Ventilation Line, detailed explanation | 54
Manual Ventilation Line, function | 51
Manual Ventilation Line, manual vent bag connection | 93
Messages, informational, Auto Air Calibration Required | 198
Messages, informational, Calibration Due | 206
Messages, informational, Cassette Will Expire in 2 Hours | 206
Messages, informational, Incomplete Calibration | 198
Messages, informational, Service Due Date within 14 Days | 205
Mixer, assembly | 84
Mixer, definition | 20
Mixer, Function | 52
Mixer, principles of operation | 37
Modes of Operation, console | 56
Monitoring, gas | 33, 37
Monitoring, gas sensor | 37
Monitoring, NO, NO2 and O2 concentrations and water trap | 82
Monitoring, patient | 7
Mount, transport | 140
MR exclusion zone | 133
MR Image Artifact | 247
MR Scanner Room | 133
MR Signal to Noise Ratio | 247
Nebulizers | 95
NO Injection Line, detailed explanation | 54
NO Injection Line, Function | 51
NO Injection Line, NO port connection | 94
Notes | 3, 174, 178
Notes, user responsibility | 32
PARTS / COMPONENTS, GENOSYL DS | 23
Pneumatic Nebulizers | 10, 95
Power connection to console | 100
Power, battery specifications | 245
Power, black rocker switch powering on | 101
Power, cord | 100
Power, EMI/EMC | 249
Power, EMI/EMC specifications | 249
Power, power down before cleaning | 226
Power, power supply | 245, 248
Power, power supply specifications | 245
Power, screen does not turn on | 208
Power, silver power button, powering on | 101
Power, system does not shutdown | 208
Pressure, operating pressure | 247
Pressure, storage/transport | 247
Problems, see Troubleshooting | 208
Procedure, adjusting the dose | 113
Procedure, air calibration | 217
Procedure, cart/console storage | 228
procedure, cassette activation | 110
Procedure, cassette disposal | 128
Procedure, cassette insertion | 101, 155
Procedure, cassette/accessory storage | 228
Procedure, cleaning | 226
Procedure, console connections | 86
Procedure, console shutdown | 124, 167
Procedure, console startup | 100
Procedure, console use as a backup | 120
Procedure, emptying the water trap | 224
Procedure, gas lines connections | 86
Procedure, GENOSYL DS ventilator circuit connections | 91
Procedure, injection assembly assembly | 83, 149, 152
Procedure, manual ventilator bag connector | 93
Procedure, mechanical ventilator circuit connections | 91
Procedure, mixer assembly | 84
Procedure, NO Calibration | 218
Procedure, NO2 calibration | 220
Procedure, resuming primary dosing after manual mode | 119, 166
Procedure, ventilatory circuit assembly pre-check | 81
Procedure, water trap replacement | 225
Procedure, weaning | 113
Pumps, general information | 33
Pumps, louder than normal | 208
Pumps, NO delivery into the ventilator system | 33
Pumps, noise level | 208
Removal, cassette prior to shutdown | 124, 167
Removal, water trap from console to empty | 224
Removal, water trap from console to replace | 225
Responsibility, User | 32
Sample Line Filter Connection | 89
Sample Line Leak test | 68
Sample Line, detailed explanation | 54
Sample Line, function | 51
Sample Line, leak test | 105, 158
Sample Line, sample tee connection | 95, 149, 152, 179
Sample Line, water trap connection | 86
Sensors, calibration | 216
Sensors, principles of operation | 37
Service, battery replacement | 245
Service, due date within 14 days | 205
Service, due date within 2 days | 205
Service, repair of replacement | 32
Service, scheduling | 222
Service, service required alarm | 194, 198
Service, yearly | 222
Shutdown Cassette Status Indicators | 69
Specification, GaussAlert | 247
Specifications, transport mount | 143
Storage, cart and console | 228
Storage, cassette | 228
Temperature, operating temperature | 247
Temperature, storage/transport | 247
Transport equipment weight | 143
Transport Mount | 144
Transport mount specifications | 143
Transport, environmental | 247
Transport, environmental specifications | 247
Ventilator Compatibility | 236
Ventilator, circuit assembly pre-check | 81
Ventilator, minute volume | 234
Ventilator, oxygen dilution | 232
Warning, user responsibility | 32
Warnings | 3, 68, 124, 167
Water Trap Leak Test | 68
Water trap, emptying | 224
Water Trap, maintainance schedule | 222
Water Trap, replacing | 225
Weaning | 113
Weight, cart specifications | 246
Weight, cassette specifications | 246
Weight, console specifications | 246
Weight, transport equipment | 143
Width and Length, cart specifications | 246
Width and Length, cassette specifications | 246
Width and Length, console specifications | 246

VERO Biotech and GENOSYL are registered trademarks of VERO Biotech Inc.
© 2025 VERO Biotech. Printed in U.S.A. LBL-602502 Rev I JUNE 2025
Please read full prescribing information enclosed.
877.337.4118 | VERO-biotech.com

INSTRUCTIONS FOR USE

VĒRO
BIOTECH

GENOSYL®
DELIVERY SYSTEM

FOR DELIVERY OF
GENOSYL®
(NITRIC OXIDE)
GAS FOR INHALATION

QUICK REFERENCE GUIDE

Technical Support: 877.337.4118

GENOSYL®DS |  | QUICK REFERENCE GUIDE

TABLE OF CONTENTS
TABLE OF CONTENTS |  | 2
LIST OF TABLES |  | 3
LIST OF FIGURES |  | 4
1. | SYSTEM SET-UP AND CONNECTIONS | 6
1.1. | GENOSYL DS Set-Up and Mechanical Ventilator Circuit Schematic | 6
1.2. | Connections to Various Breathing Systems | 7
1.2.1 | Conventional Ventilators | 7
1.2.2 | Non-Invasive Gas Delivery Systems | 10
1.3 | GENOSYL DS Ventilator Circuit Assembly Pre-Check | 12
1.4 | Assembling GENOSYL DS Injection Assembly with Adaptive Sensor | 13
1.4.1 | GENOSYL DS Injection Assembly with Adaptive Sensor | 13
1.4.2 | GENOSYL DS Mixer Assembly with Adaptive Sensor | 13
1.5 | GENOSYL DS Console Connections | 14
1.5.1 | GENOSYL DS Gas Lines Connections | 14
1.5.2 | GENOSYL DS Sample Line Extension Connection | 16
1.5.3 | GENOSYL DS Respiratory Circuit Connections | 17
1.6 | Manual Ventilation (Bag) Connection | 18
1.7 | Mechanical Ventilator Circuit Connections | 18
2. | SYSTEM START UP | 19
2.1 | Console Start-Up | 19
2.2 | Cassette Insertion & Water Trap / Sample Line Leak Test | 20
3 | NITRIC OXIDE ADMINISTRATION | 21
3.1 | Nitric Oxide Dose Set-Up and Administration | 21
3.1.1 | Setting a dose when using a circuit with an Adaptive Sensor | 21
3.1.2 | Setting the dose when using a circuit without an Adaptive Sensor | 22
3.2 | Replacement of a Depleted Cassette | 22
3.3 | Manual Dosing Mode | 23
3.3.1 | Manual Ventilation Use (Bagging) | 23
3.4 | Resuming Primary Dosing | 24
3.5 | Adjusting the Dose | 24
3.5.1 | Adjusting the Dose when using a Circuit with an Adaptive Sensor | 24
3.5.2 | Adjusting the Dose and Flow Range when using a Circuit without an Adaptive Sensor | 24
3.6 | Console Use as a Back-Up | 25
4 | CONSOLE SHUTDOWN AND CASSETTE DISPOSAL | 25
4.1 | Console Shutdown | 25
4.2 | Cassette Disposal | 27
5 | ALARMS, ALERTS, AND TROUBLESHOOTING | 27
5.1 | Alarms, Alerts, and Troubleshooting | 27
6 | MAINTENANCE | 28
6.1 | Calibration | 28
6.1.1 | Air Calibration | 29
6.1.2 | NO Calibration | 29
6.1.3 | NO2 Calibration | 30
6.2 | Maintenance Schedule | 30
6.3 | Water Trap Maintenance | 31
6.3.1 | Emptying the Water Trap | 31
6.3.2 | Water Trap Replacement | 31
6.4 | Battery | 32
6.5 | Cleaning | 32
6.5.1 | Enclosure, Connections, and Surfaces Other Than the Display | 32
6.5.2 | Display Screen | 33
6.6 | Storage | 33
6.6.1 | Cart / Console Storage | 33
6.6.2 | Cassette / Accessory Storage | 34
6.7 | Ventilator Compatibility | 34

LIST OF TABLES
Table 1: | Conventional Ventilator Compatibility Test Ranges | 8
Table 2: | Non-Invasive Gas Delivery System Compatibility Test Ranges | 10
Table 3: | Details of Validated Systems | 35
Table 4: | Validated Compatibility with and without Inline Mixer | 39

LIST OF FIGURES
Figure 1: | Front View GENOSYL DS Console | 5
Figure 2: | GENOSYL DS Display Screen | 5
Figure 3: | Conventional Ventilator Circuit Set-Up and Connections using Injection Assembly with Adaptive Sensor to the GENOSYL DS and a Manual Bagging System | 9
Figure 4: | Conventional Ventilator Circuit Set-Up and Connection using the Mixer Assembly with Adaptive Sensor to the GENOSYL DS and a Manual Bagging System | 9
Figure 5: | Fisher and Paykel Optiflow Jr 2 Breathing Circuit Diagram | 11
Figure 6: | Fisher and Paykel Optiflow Breathing Circuit | 11
Figure 7: | GENOSYL DS Injection Assembly with Adaptive Sensor | 13
Figure 8: | GENOSYL DS Mixer Assembly with Adaptive Sensor | 14
Figure 9: | Manual Ventilation System | 18

1. SYSTEM SET-UP AND CONNECTIONS

1.1. GENOSYL DS Set-Up and Mechanical Ventilator Circuit Schematic

NOTE: Naming conventions: The GENOSYL DS accessories and components consist of the GENOSYL DS Injection Assembly with Adaptive Sensor or GENOSYL DS Mixer Assembly with Adaptive Sensor, and the GENOSYL DS Gas Lines. Refer to Section 6.7 Table 4for when use of the Mixer Assembly with Adaptive Sensor is recommended.

NOTE: All circuit components, including GENOSYL DS circuit components, should be changed out according to hospital protocol.

WARNING:

- ALWAYS use the GENOSYL DS in accordance with the indications, usage, contraindications, warnings, and precautions described in the GENOSYL prescribing information and labeling. Refer to latest approved prescribing information and labeling prior to use.
- The approved patient population for the GENOSYL DS as specified in the drug labeling for GENOSYL (nitric oxide) for inhalation, is limited to neonates. The GENOSYL DS is not intended to be used in other patient populations.
- ONLY use the GENOSYL DS, its parts, and accessories as instructed. Using non-specified components may result in product malfunction, injury or death.
- ALWAYS follow pre-use setup instructions for the routing and connections of tubing to avoid patient strangulation.
- MAKE SURE the System has all tubing connected as described in the instructions. Not connecting all tubing may result in inaccurate dosage and harm to the patient.
- DO NOT use accessories or cables other than those specified or provided by the manufacturer of this equipment, as this may result in increased electromagnetic emissions or decreased electromagnetic immunity of this equipment and result in improper operation.

1.2. Connections to Various Breathing Systems

1.2.1 Conventional Ventilators

- Bio-Med Devices CrossVent 2+
- Bio-Med Device MVP-10
- Dräger V500
- Dräger VN500
- Dräger V600
- Dräger VN600
- Dräger V800
- Dräger VN800
- Hamilton C1/T1
- Hamilton C6
- Hamilton G5
- Hamilton MR1
- Puritan Bennett 980
- Vyaire AVEA

WARNING:

- ONLY use the GENOSYL DS with Bio-Med Crossvent 2+ with Constant Flow ON. Not doing so may lead to elevated NO2levels or dose variability.
- The GENOSYL DS injects and samples gas from the patient respiratory circuit which may affect the triggering sensitivity of the ventilator. ALWAYS ensure the trigger sensitivity of the ventilator is checked after connecting the GENOSYL DS to the breathing circuit or when the dose is changed and adjust trigger sensitivity as necessary. Failure to do so may lead to ventilator auto cycling or apnea alarm.
- ALWAYS ensure the patient disconnect and high–pressure alarms are used with the ventilator.

CAUTION:

- When using spontaneous breathing modeson respiratory device, NO2levels may exceed 3.0 ppm when dosing ≥ 57 ppm NO into 100% FiO2and maximum bias flow resulting in nitric oxide delivery interruption. Once sample value of NO2is below 3.0 ppm, the Console will auto resume delivery of NO at set dose. Refer to the Operator's Manual Section 12.1.5 Table 13 for additional information.
- When using non-spontaneous breathing modeson respiratory device, NO2levels may exceed 3.0 ppm when dosing ≥ 63 ppm NO or greater into 100% FiO2and maximum bias flow resulting in nitric oxide delivery interruption. Once sample value of NO2is below 3.0 ppm, the Console will auto resume delivery of NO at set dose. Refer to the Operator's Manual Section 12.1.5 Table 13 for additional information.

Table 1: Conventional Ventilator Compatibility Test Ranges
Setting | Range | Unit
Inspiratory Flow Rate | 2-120 | LPM
Respiratory Rate | 6-60 | BPM
Peak Inspiratory Pressure | 0-70 | cmH2O
Positive End-Expiratory Pressure (PEEP) | 0-20 | cmH2O

For applicable use scenarios, and when use of a mixer is required, see Section 6.7, Table 4.

1.2.2 Non-Invasive Gas Delivery Systems

- Fisher and Paykel Optiflow Jr Breathing Circuit
- Fisher and Paykel Optiflow Breathing Circuit

Table 2: Non-Invasive Gas Delivery System Compatibility Test Ranges
Setting | Range | Unit
Fisher and Paykel Optiflow Jr 2 Flow Rate | 0.5 - 25 | LPM
Fisher and Paykel Optiflow Flow Rate | 5-60 | LPM

For applicable use scenarios, see Section 6.7, Table 4.

1.3 GENOSYL DS Ventilator Circuit Assembly Pre-Check

Follow the steps listed below for the initial System pre-check prior to completing the ventilator circuit assembly.

1. Removeall items of the GENOSYL DS Parts / Components from packaging.
2. Checkthe expiration date for each Cassette and Inline Breathing Circuit Filter to ensure use is within the expiration date.

WARNING:DO NOT use a Cassette that is beyond its expiration date. Using an expired Cassette may affect the Cassette's ability to provide the correct NO dosage to the patient, which may cause injury or death.

- Visuallyinspectthe Water Traps on both Consoles to ensure they are installed and empty (Note: To empty the Water Trap, see Section 6.3.1).

WARNING:

- ALWAYS empty Water Trap before each use, when prompted by the System, and when the trap is more than half full. Allowing the Water Trap to completely fill will occlude the Sample Line which will interrupt patient gas NO, NO2, and O2concentration monitoring. Failure to monitor the patient gas NO, NO2, and O2concentrations may result in patient injury.
- ALWAYS conduct Water Trap /Sample Line Leak Test every time you empty and replace the Water Trap, as failure to do so may lead to an incorrect NO reading, which can result in injury or death.

1.4 Assembling GENOSYL DS Injection Assembly with Adaptive Sensor

The Injection Assembly with Adaptive Sensor or the Mixer Assembly with Adaptive Sensor is the point of nitric oxide injection into the patient respiratory circuit. Only one type of assembly is required for each patient circuit. For certain scenarios, the Mixer Assembly with Adaptive Sensor is recommended to mix the NO gas with the gas supplied by the ventilator through a filter containing silica gel to provide intra-breath NO delivery. Refer to Table 4 for scenarios when a Mixer is recommended for use.

NOTE: When using a Mixer, an Inline Breathing Circuit Filter must be used. If a Mixer is not used, an Inline Breathing Circuit Filter as presented in Figure 8may be used, or an Injection Line Filter connected to the port on the Gas Injection Adapter may be used.

1.4.1 GENOSYL DS Injection Assembly with Adaptive Sensor

1. Connectthe Inline Breathing Circuit Filter to the Gas Injection Adapter (22mm ID × 22 mm OD).
2. ConnectAdaptive Sensor to the inlet end of Gas Injection Adapter (22mm ID × 22 mm OD).

1.4.2 GENOSYL DS Mixer Assembly with Adaptive Sensor

- Connectthe Inline Breathing Circuit Filter to the Adapter (22mm ID × 22 mm OD).
- Connectthe Adapter (22mm ID × 22 mm ID) to the distal end of the Mixer.
- Connectthe Gas Injection Adapter to the proximal end of the Mixer.
- ConnectAdaptive Sensor to the proximal end of the Gas Injection Adapter.

NOTE: To determine if the Injection Assembly with Adaptive Sensor or the Mixer Assembly with Adaptive Sensor is recommended, see Section 6.7, Table 4.

1.5 GENOSYL DS Console Connections

1.5.1 GENOSYL DS Gas Lines Connections

Follow the steps listed below to connect the Gas Lines to both Consoles.

1. Pushand twistclockwise the short Y-end of the NO Injection Line (red) to the "NO" port (red)on the front panel of the dosing Console.
2. Pushand twistthe short Y-end of the Sample Line (blue) to the Gas Sample Port (blue)on the front of the Water Trap, attached to the dosing Console.
  NOTE:Ensure the Sample Lines are connected to the Water Traps on both Consoles.
3. Pushand twistthe short Y-end of the Manual Ventilation Line (clear) to the Manual Bagging Port on the front of the dosing Console.
4. Repeatsteps 1, 2, and 3 on the Back-up Console.
5. ConnectAdaptive Sensor Cable to Adaptive Sensor Port on front of the dosing Console.

1.5.2 GENOSYL DS Sample Line Extension Connection

For use in the MR Environment when a longer sample line may be required, follow the steps listed below to connect a Sample Line Extension. It is recommended to install the extension prior to initiation of dose.

1. If actively dosing, switchto Manual Dosing Mode prior to completing the following steps.

WARNING:Failure to switch to Manual Dosing Mode prior to installing a Sample Line Extension when the System is actively dosing may result in a spike in the NO dose delivered to the patient.

1. Turnthe blue Stopcock Valve, attached at the Gas Sample Tee, to the closed position as shown.

- Pushand twistcounterclockwise the Luer-Lock Collar of the Sample Line to remove from the blue Stopcock Valve at the Gas Sample Tee.

1. Pushand twistclockwise the Luer-Lock Collar of the Sample Line onto the Sample Line Extension female connection.
2. Pushand twistclockwise the Luer-Lock Collar of the Sample Line onto the blue Stopcock Valve at the Gas Sample Tee.
3. PerformWater Trap/Sample Line Leak test, as instructed.

- If actively dosing, switchback to Primary Dosing Mode

1.5.3 GENOSYL DS Respiratory Circuit Connections

Follow the steps listed below to connect the Gas Lines to the Injection Assembly, Sample Tee, and Adaptive Sensor. If a Sample Tee already exists within the ventilator circuit, the Sample Line may be connected directly to the existing Sample Tee.

1. Pushand twistclockwise the Luer-Lock Collar from the NO Injection Line onto the NO Injection Assembly.

NOTE:After connecting, the valve assembly may have rotated such that the orientation may appear different from what is shown here and on the display screen.

1. Pushand twistclockwise the Luer-Lock Collar of the Sample Line onto the Sampling Port of the Gas Sample Tee.

NOTE: Skip this step if a Gas Sample Tee is already connected and in-line with the ventilator circuit.

1. Ensurethe blue Stopcock Valve is in the open position as shown.

- Connectthe distal end of the Adaptive Sensor Cable to the Adaptive Sensor on the Injection Assembly

1.6 Manual Ventilation (Bag) Connection

1. Attachthe barbed end of the Manual Ventilation Bag NO Adapter into the oxygen tubing from the oxygen source.
2. Attachthe other end of the NO Adapter to the oxygen port on the side of the Manual Ventilation Bag.
3. Connectthe Manual Ventilation Line (clear) to the NO Injection Port of the Manual Ventilation Bag NO Adapter.
4. Placethe Manual Ventilation Assembly in a clean accessible place if needed for future use.

1.7 Mechanical Ventilator Circuit Connections

Follow the steps outlined in this section to connect the GENOSYL DS Ventilator Circuit Assembly to the Mechanical Ventilator Circuit.

WARNING:

- The GENOSYL DS injects and samples gas from the patient respiratory circuit which may affect the triggering sensitivity of the ventilator. ALWAYS ensure the trigger sensitivity of the ventilator is checked after connecting the GENOSYL DS to the breathing circuit or when the dose is changed and adjust trigger sensitivity as necessary. Failure to do so may lead to ventilator auto cycling or apnea alarm.
- ALWAYS ensure the patient disconnect and high–pressure alarms are used with the ventilator.

NOTE: All ventilator connections should be assembled and inspected prior to connecting to the mechanical ventilator circuit.

1. Disconnectthe Inspiratory Tubing from the humidifier and attach it to the proximal end of the Injection Assembly to the Adaptive Sensor.
2. Attachthe distal end of the Injection Assembly to the humidifier.
3. Insertthe Sample Tee into the ventilator circuit at the proximal end of the temperature probe closest to the patient.

2. SYSTEM START UP

2.1 Console Start-Up

CAUTION:

- ONLY use the GENOSYL DS with the power cord supplied by the manufacturer. Use of a generic power cord may cause output voltage instability leading to a touch screen failure.
- ALWAYS ensure the power cord is firmly seated into the power supply and the wall outlet. A loose connection can result in damage to the device or faulty operation.

1. Pushthe Circular Power Connectors into the back of the top and bottom Consoles.
2. Connectthe main power cord to a grounded 120 V electrical outlet.
3. Pressthe Black Rocker Power Switch, located on the back of each Console, to the right (ON position) to power on both Consoles.
4. Pressthe Silver Power Button, located at the top left corner on the front panel of eachConsole, to turn on the display screens on both Consoles. The display screen will illuminate, and the Consoles will beep, indicating the power is on.

CAUTION:The System will conduct an internal self-test. If an alarm or failure message should occur, refer to Section 10 in the Operator's Manual to resolve the issue.

NOTE: If the display screen does not turn on, see Troubleshooting, Section 10of the Operator's Manual.

2.2 Cassette Insertion & Water Trap / Sample Line Leak Test

The following steps should be taken on both the top and bottom Consoles. Upon the insertion of the Cassette, a test will be initiated on each Console to check and ensure the integrity of the Water Traps and Sample Line.

The Water Trap / Sample Line Leak Test is automatically initiated when a Cassette has been inserted,and the measured NO is less than 1.0 ppm.

WARNING:ALWAYS follow Cassette insertion instructions prior to Cassette insertion. Not inspecting the Cassette prior to insertion may lead to using a faulty Cassette, resulting in injury.

1. Confirmthe Cassette State Window on each Cassette is blue.

WARNING:DO NOT use the Cassette if the Cassette State Window is not blue. A Cassette State Window that is any color other than blue may affect the Cassette's ability to provide the correct NO dosage to the patient, which may cause injury or death.

NOTE: If the Cassette State Window is not blue, see Troubleshooting, Section 10.8of the Operator's Manual.

1. Openthe Cassette Access Doors and inserttwo Cassettes into the Dosing Console and at least one Cassette into the Back-Up Console. Push until it clicks.

NOTE: The Water Trap / Sample Line Leak Test is automatically initiated when a Cassette has been inserted,and the measured NO is less than 1.0 ppm
After the first Cassette is fully inserted, the Operator will have 60 seconds to close the blue Stopcock Valveto perform the test.

1. Followthe onscreen instructions on both Consoles.

NOTE:

- The screen will indicate the Water Trap / Sample Line Leak Test has started and the progress bar will be red until the stopcock valve has been closed, upon which it will then turn green if there is no leak detected.
- See Section 3.5for detail around dosing in Manual Dosing Mode.

1. Followthe onscreen instructions on both Consoles.

CAUTION: Open the blue Stopcock Valve priorto pressing "Accept". Failure to do so will result in a line occlusion error.

NOTE:If the Water Trap / Sample Line Leak Test fails, follow the onscreen instructions to resolve the issue. Also see Troubleshooting, Section 10.8of the Operator's Manual.

1. If this screen is displayed, followthe onscreen instructions on both Consoles .
2. PressYes on both Consoles to begin a new Water Trap / Sample Line Leak Test.

3 NITRIC OXIDE ADMINISTRATION

3.1 Nitric Oxide Dose Set-Up and Administration

WARNING:

- MAKE SURE the System stabilizes to the prescribed concentration (ppm) of NO prior to leaving the Console unattended. Failure to do so could result in under delivery of the target NO, leading to injury or harm.
- ALWAYS constantly monitor the patient. System malfunctions can occur if device and patient are not monitored and can result in injury or death. Careful monitoring is required by care personnel whenever the System is used on a patient. The use of an alarm and a monitoring system does not give an absolute assurance of warning for every malfunction that may occur. Certain alarms may require immediate response.
- If the gas flow of the patient's respiratory device/ventilator should be interrupted or discontinued, the NO dose should be maintained by switching to Manual Dosing Mode or the target NO dose should be set to zero.

3.1.1 Setting a dose when using a circuit with an Adaptive Sensor

1. Pressthe gray "Set" button on the display screen.
2. Enterthe prescribed dose in ppm on the electronic keypad.
3. PressOK to confirm the entry.

3.1.2 Setting the dose when using a circuit without an Adaptive Sensor

1. Pressthe gray "Set" button on the display screen.
2. ConfirmTotal Flow Range is appropriately selected.
3. Enterthe prescribed dose in ppm on the electronic keypad.
4. PressOK to confirm the entry.

NOTE:

- The time to reach target dose may vary up to 10 minutes.
- If unable to set the dose in Primary Dosing Mode, see Troubleshooting, Section 10.8of the Operator's Manual.

3.2 Replacement of a Depleted Cassette

The GENOSYL DS automatically switches from the dosing Cassette to the secondary Cassette in the Dosing Console once the Cassette is depleted, when a secondary Cassette is properly inserted and preheated. After transition, the depleted Cassette is automatically ejected.

CAUTION:User should always have a secondary Cassette inserted in Dosing Console and preheated in order for auto transition to occur. User should replace depleted Cassette as soon as possible after ejection.

ILLUSTRATION

ACTION

Warnings, Cautions and Notes

NOTE

The Console will automatically transition to the secondary Cassette if properly inserted and preheated. The screen to the left will be displayed during the transition process.

3.3 Manual Dosing Mode

NOTE: When entering Manual Dosing Mode, the set target dose in Primary Dosing Mode will carry over to Manual Mode if 5 ppm or greater. Less than 5 ppm set target dose in Primary Dosing Mode will default to 5 ppm dose in Manual Dosing Mode. However, dose and flow rate be adjusted for specific situations. The GENOSYL DS Smart Feedback System™ is disabled while in Manual Dosing Mode. To reinitiate the feedback loop, switch back to Primary Dosing Mode as soon as the situation permits

3.3.1 Manual Ventilation Use (Bagging)

WARNING:

- ALWAYS ensure that the manual flow displayed on the Console matches the flow set into the resuscitation bag. Incorrect flow settings may result in an incorrect estimation of NO delivery. If the flow into the manual equipment is too low, there is risk of overdosing the patient with NO.
- ALWAYS squeeze the bag several times, after starting fresh gas flow, to empty residual gas in the bag prior to using the System to ventilate a patient. Failure to do so could result in higher NO2 levels being delivered to the patient.
- ALWAYS use the smallest bag adequate to deliver the desired tidal volume. Failure to do so could result in higher NO2 levels being delivered to the patient.
- ONLY use a manual resuscitation bag with the GENOSYL DS for a short time (e.g., less than one hour) when on battery only. Otherwise, the System may shut off and may result in injury or death.
- If the dilution flow rate displayed on the screen does not match the wall source, then the estimated NO may be inaccurate.

1. Ensurethe oxygen source is set appropriately or adjust as needed.
2. Pressthe button "Switch to Manual" on the Dosing Console.
3. Press"Confirm" to switch to Manual Dosing Mode
4. To resumeprimary dosing, see Section 3.4.

NOTE:

- When switching to Manual Dosing Mode, dosing has been initiated at the same dose (ppm) as set in Primary Dosing Mode. If the dosing was set at "0" prior to pressing the "Switch to Manual" button, the estimated NO will also be at "0" and will need to be adjusted. If the primary dosing was set between 1 and 5 ppm prior to pressing the "Switch to Manual" button, the estimated NO dose will also be 5 ppm and may be adjusted.
- If an adjustment of the NO concentration is required, press the green up and down arrows.
- If an adjustment to the Dilution Flow Rate is required, press the LPM value and a drop-down menu will expand. Press the prescribed value. The new value will be highlighted in blue and the drop-down menu will collapse.
- In the event dose is initiated in Manual Dosing Mode, the Console will default to 20 ppm, which can be adjusted as needed.

3.4 Resuming Primary Dosing

1. Pressthe "Switch to Primary" button at the top of the Manual Dosing Mode screen.
2. Press"Confirm" to start dosing or "Cancel" to cancel.

NOTE:The NO dose used in Manual Dosing Mode will become the set target dose in Primary Dosing Mode.

3.5 Adjusting the Dose

To adjust the dose of nitric oxide administered per hospital protocol/physician order. Follow the instructions listed below.

3.5.1 Adjusting the Dose when using a Circuit with an Adaptive Sensor

1. Pressthe gray "Set" button to access the electronic keypad on the display screen on the Dosing Console.
2. Enterthe prescribed (ppm) dose using the electronic keypad.
3. Press"OK" to confirm the dose and to start dosing administration.

3.5.2 Adjusting the Dose and Flow Range when using a Circuit without an Adaptive Sensor

1. Pressthe gray "Set" button to access the electronic keypad on the display screen on the Dosing Console.
2. Enterthe prescribed (ppm) dose using the electronic keypad.
3. AdjustTotal Flow Range, if necessary.
4. Press"OK" to confirm the dose and to start dosing administration.

3.6 Console Use as a Back-Up

This section describes the process of activating the Cassette in the Back-Up Console. Delivery of NO will begin immediately upon Cassette activation.

1. Pressthe "Set" button on the Back-Up Console which will display the NO dose electronic keyboard and Flow Section menu.
2. ConfirmDose and Total Flow range is appropriately selected.
3. Press"OK" to confirm entry
4. ConnectAdaptive Sensor to the front of the new Dosing Console

NOTE:

- The default Total Flow range displayed will be <2.5 LPM unless otherwise selected by the user.
- The Back-Up Console is now the and Flow Range Console.
- Dosing has been initiated at the default setting of 20 ppm.

4 CONSOLE SHUTDOWN AND CASSETTE DISPOSAL

WARNING:NEVER turn the rear power switch OFF until the System has gone through a controlled shutdown or instructed by VERO Technical Support. Turning the rear power switch OFF prematurely (e.g., while it is still in use) will immediately shut down the device. This may result in interruption in NO delivery to the patient, which may cause injury or death.

CAUTION:

- NEVER turn the rear power switch OFF until the System has gone through a controlled shutdown or instructed by VERO Technical Support. Turning the rear power switch OFF prematurely (e.g., while it is still in use) will immediately shut down the device and may cause improper operation upon restart.

4.1 Console Shutdown

If the administration of NO must be stopped, then the dose level must be set to "0" and the Cassette must be removed prior to shutting down the Console.

1. Pressthe gray "Set" button to access the electronic keypad on the display screen.
2. Setthe dose to "0" using the electronic keypad.
3. Press"OK" to confirm the entry.
4. If the "Settings" tab is not displayed, pressthe "Menu" tab to access the sub-level tabs.
5. Pressthe "Settings" tab on the display menu.
6. Pressthe red "System Shut Down" icon.
7. Reviewon screen prompt .
  NOTE:The screen will inform user if Cassette should be saved or disposed of.
8. Press"Confirm" to confirm shutdown.
9. Waituntil the Console shuts down, the display screen appears blank, and the Console emits an audible beep.
  NOTE:The Console will inert any remaining contents from a dosing Cassette upon ejection rendering it unusable. If a Cassette has only been preheated, and not used for dosing, the contents have not been inerted and it can still be used.
10. Openthe Cassette Access Door.
11. Removethe Cassette by pulling the Cassette straight out.
12. Disposethe Cassette per hospital policy.
13. Pressthe Black Rocker Power Switch to the "OFF" position.
14. R epeat steps 1-12 for the other Console.

WARNING: NEVER turn the rear power switch OFF until the System has gone through a controlled shutdown or instructed by VERO Technical Support. Turning the rear power switch OFF prematurely (e.g., while it is still in use) will immediately shut down the device. This may result in interruption in NO delivery to the patient, which may cause injury or death.

CAUTION:NEVER turn the rear power switch OFF until the System has gone through a controlled shutdown or instructed by VERO Technical Support. Turning the rear power switch OFF prematurely (e.g., while it is still in use) may cause improper operation.

NOTE: If the System does not shut down, see Troubleshooting, Section 10.8of the Operator's Manual.

4.2 Cassette Disposal

Following dosing use, any remaining Cassette liquid contents are purged into an inerting chamber that is built into the Cassette, where the contents are chemically neutralized, rendering the Cassette safe for disposal. When the Cassette liquid contents are emptied into the inerting chamber, the Cassette State Window on the front of the Cassette reddens and bleaches from its original blue color, indicating the Cassette is depleted. The Cassette can now be disposed of per hospital policy.

5 ALARMS, ALERTS, AND TROUBLESHOOTING

WARNING:ALWAYS ensure patient safety before troubleshooting (such as an activated alarm) or replacing a problematic item. Not monitoring the patient prior to attending to an alarm can result in injury or death.

5.1 Alarms, Alerts, and Troubleshooting

Section 10 of the Operator's Manualcontains the system alarms and message in order of High (red), Medium (yellow), and Low Priority (turquoise) followed by Informational Messages (green). The table shows the alarm/symptom, the possible cause(s) of the alarm and recommended action to resolve the alarm. Additionally, on-screen troubleshooting support is available by either tapping an active alarm banner or by selecting the "Alarm Info" button on the "Alarms" tab. If the alarm/issue cannot be resolved, contact Technical Support at 877-337-4118.

A sample screen with an active alarm is shown below:

The alarm banner contains a drop-down menu containing a list of all alarms should there be multiple activated. The alarm icon is always present on the top right of the screen and tapping the icon will pre-silence or silence alarms. Refer to the table below for descriptions of each alarm status:

ALARM ICON DISPLAY

DESCRIPTION

No active alarm condition is detected on the Console. Tap this icon to activate the pre-silence feature.

Alarms are actively pre-silenced. Countdown of time remaining appears under the icon. Pre-silence lasts for 120 seconds. Low/High NO, High NO2, Low/High O2, Water Trap Removed and Dosing Cassette Removed alarms are pre-silenced. Alarms will still be visible on alarm banner but audible alarm will not sound.

Console has an active alarm condition that requires attention. Tap the icon to silence the alarm for 120 seconds.

Console has an active alarm condition that requires attention and the alarms have been silenced. Countdown of time remaining appears under the icon.

6 MAINTENANCE

6.1 Calibration

WARNING:

- ONLY use the calibration gas pressure regulators supplied by the manufacturer. Pressure regulators not supplied by the manufacturer may damage the sensors and may lead to patient injury.
- ALWAYS verify the correct NIST traceable calibration gas is being used and confirm the expiration date of the calibration gas prior to performing calibration. The use of incorrect or expired gas may result in inaccurate sensor readings and can lead to patient injury.
- NEVER perform NO or NO2 calibration within the MR scanner room. Calibration equipment is a potential projectile hazard.

CAUTION:

- ALWAYS perform a full-scale calibration of the GENOSYL DS when prompted by the System prior to use.
- ALWAYS confirm the correct flow direction of the installed one-way check valve in the sampling tee to avoid over pressurization of the sampling system and damage to the device.

6.1.1 Air Calibration

Air Calibration will take up to 2 minutes. A progress bar is displayed in the lower lefthand corner of the display screen during the calibration process.

1. Checkto make sure nothing is connected to the CAL port during Air Calibration.
2. If the "Calibration" tab is not displayed, pressthe "Menu" tab to access the sub-level tabs.
3. Pressthe "Calibration" tab on the display menu.
4. Pressthe Low Range "Air" button.
5. Pressthe blue "Start Calibration" button.
6. Press"Accept " to continue once calibration is complete.

NOTE: If calibration fails, ensure that nothing is connected to or blocking the CAL port.

6.1.2 NO Calibration

WARNING:

- DO NOT open the valve prior to connecting to the CAL port. Opening the valve first will expose the user to NO gas.
- DO NOT interrupt calibration until finished. If interrupted, calibration will be cancelled.
- DO NOT disconnect tubing from the calibration port prior to closing the valve. Disconnecting the tubing first will expose the user to NO gas.

NOTE: NO calibration takes approximately 2 minutes if not dosing, or five minutes if actively dosing. A progress bar is displayed in the lower left-hand corner of the display screen during the calibration process.

1. If the Calibration Tab is not displayed, pressthe "Menu" tab to access the sub-level tabs.
2. Pressthe "Calibration" tab on the display menu.
3. Pressthe High Range "NO" button.
4. Pressthe blue "Start Calibration" button.
5. Followthe onscreen instructions.
6. Press"Accept " to continue once calibration is complete.

6.1.3 NO2Calibration

WARNING:

- DO NOT open the valve prior to connecting to the CAL port. Opening the valve first will expose the user to NO2gas.
- DO NOT interrupt calibration until finished. If interrupted, calibration will be cancelled.
- DO NOT disconnect tubing from the calibration port prior to closing the valve. Disconnecting the tubing first will expose the user to NO2gas.

NOTE:NO2calibration takes approximately 2.5 minutes. A progress bar is displayed in the lower left-hand corner of the display screen during the calibration process.

1. If the Calibration Tab is not displayed, pressthe "Menu" tab to access the sub-level tabs.
2. Pressthe "Calibration" tab on the display menu.
3. Pressthe High Range "NO2" button.
4. Pressthe blue "Start Calibration" button
5. Followthe onscreen instructions.
6. Press"Accept " once calibration is complete.

6.2 Maintenance Schedule

The Console components require the following maintenance:

COMPONENT | SCHEDULE
Water Trap | Per patient or as required (per Sample Line / Leak Test)
Console | 24 months or 10,000 pump hours, which ever is first

The Console requires factory service every 24 months or 10,000 pump hours, whichever is first. The System will display an Information Message to remind the operator when service is required. Call Technical Support at 877-337-4118to schedule service.

6.3 Water Trap Maintenance

6.3.1 Emptying the Water Trap

WARNING:ALWAYS empty Water Trap before each use, when prompted by the System, and when the trap is more than half full. Allowing the Water Trap to completely fill will occlude the Sample Line which will interrupt patient gas NO, NO2, and O2concentration monitoring. Failure to monitor the patient gas NO, NO2, and O2concentrations may result in patient injury.

1. RemoveWater Trap from Console by lifting latch and pulling the base of the Water Trap away from the Console.
2. Removethe lid by pulling the lid from the base.
3. Emptythe liquid contents.
4. Cleanthe Water Trap per hospital policy and cleaning instructions in the Operator's Manual.
5. Reattachthe lid by pushing it back onto base.
6. Slidethe Water Trap back on the Console until it clicks into place.

6.3.2 Water Trap Replacement

WARNING:

- ALWAYS use a Water Trap supplied by the manufacturer. Using an incorrect water trap could result in non-functioning or inaccurate sensor readings.
- ALWAYS conduct a Water Trap test every time you empty and replace the Water Trap, as failure to do so may lead to an incorrect NO reading, which can result in injury or death.

If the Water Trap / Sample Line Leak Test does not meet requirements and the Sample Line integrity is confirmed or remains occluded, replace the Water Trap.

1. Removeold Water Trap from Console by lifting the latch and pulling the base of the Water Trap away from the Console.
2. Slidenew Water Trap back on the Console until it clicks into place.
3. Discardthe old Water Trap.

6.4 Battery

The battery will be serviced during scheduled maintenance performed by the manufacturer. If the need arises to replace the battery sooner than scheduled contact Technical Support at 877-337-4118to schedule a maintenance appointment.

During storage, the GENOSYL DS may be stored with the power off, but the external power supply should be connected at least once every 3 months to ensure a minimum charge is maintained on the internal battery.

WARNING:ONLY properly trained personnel should replace the battery. Incorrectly replacing the battery may result in a hazard such as excessive temperatures, fire, or explosion.

6.5 Cleaning

CAUTION:

- ALWAYS power down the GENOSYL DS Console and disconnect the power to the Console when not in use. Failure to do so may lead to permanent damage to the Console.
- DO NOT sterilize (e.g., autoclave, gas sterilize) any of the components of the System, as this may compromise performance.
- DO NOT use harsh cleaning agents on the GENOSYL DS. Doing so may impair the structural integrity and/or function of the device.
- ONLY use a damp cloth to clean the Console and limit use of liquids around Console. Excess water can permanently damage the device.
- ALWAYS ensure the System is completely dry after cleaning before powering it ON. Failure to do so could result in equipment damage.

6.5.1 Enclosure, Connections, and Surfaces Other Than the Display

Prior to performing any cleaning or maintenance operations ensure that the GENOSYL DS Console has been completely powered down and that the AC/DC power supply external to the GENOSYL DS Console has been unplugged. Apply any mild detergent to cloth prior to wiping down the System. Gently clean the outer surface of the Console, Cart, and Adaptive Sensor Cable with a soft damp cloth and mild detergent or isopropyl alcohol (70%).

WARNING:

- NEVER submerge the GENOSYL DS, Cassette, or non-disposable Adaptive Sensor Cable. Submerging in liquid will damage the System and could cause electrical shorts which may result in injury or death.
- DO NOT clean the GENOSYL DS with the power connected and the System turned ON, as this may lead to injury (e.g., shock). Unplug AC/DC power supply external to the System prior to cleaning.

6.5.2 Display Screen

Turn off Console and disconnect from AC power. Gently clean with a damp cloth.

CAUTION:

- DO NOT touch or rub the display screen with abrasive cleaning compounds or organic solvents, as they may scratch and damage the screen.
- DO NOT spray or pour liquids directly on the controller or the display, as they may damage the screen.

6.6 Storage

6.6.1 Cart / Console Storage

The acceptable storage conditions for the cart/Console are shown in the following table.

Cart / Console Storage | Temperature | -20°C to 60°C
Cart / Console Storage | Humidity | 15% to 95%, non-condensing
Cart / Console Storage | Pressure | 57kPa to 110kPa

During storage, the GENOSYL DS may be stored with the power off, but with the external power supply connected in which case the internal battery will be kept fully charged.

During storage, the GENOSYL DS may be stored with the power off, but the external power supply should be connected at least once every 3 months to ensure a minimum charge is maintained on the internal battery.

WARNING:

- MAKE SURE the GENOSYL DS is connected to AC wall power to charge the battery a minimum of once every 3 months to maintain a minimum battery charge. Failure to recharge the Console battery for extended timeframes may result in full discharge of the battery. If a Battery Error message occurs during startup of the System, contact Technical Support at 877-337-4118for assistance.
- ONLY properly trained personnel should replace the battery. Incorrectly replacing the battery may result in a hazard such as excessive temperatures, fire, or explosion.
- ONLY store the GENOSYL DS as outlined in the storage instructions. Not storing the device in alignment with its storage instructions can cause the device to be unsafe and lead to injury or death.

6.6.2 Cassette / Accessory Storage

The GENOSYL DS may not function correctly if the Cassette or any of the System Accessories have been exposed to high levels of heat or humidity. Cassettes are supplied in a plastic container and should remain unopened until use. Cassettes should be stored at 25°C (77°F) with excursions permitted between 15°C to 30°C (59°F to 86°F). (See USP Controlled Room Temperature)

6.7 Ventilator Compatibility

Vero Biotech performs validation testing which determines the compatibility of ventilator/gas delivery systems with the GENOSYL DS. During this compatibility testing, the GENOSYL DS is evaluated for the following parameters while connected to each ventilator/gas delivery system:

- NO Dose Accuracy:Continuous and accurate delivery of a targeted dose of nitric oxide within ± 20% of setpoint or within +/- 2 ppm, whichever is greater.
- Respiratory Device Gas Delivery and Alarms:The respiratory device breath delivery and alarms continue to function as intended by the manufacturer across the range of operating conditions.
- NO2Performance: NO2remains within acceptable limits less than 1.0 ppm with 60% FiO2 and ≤40 ppm NO.
- O2Dilution: Post dilution O2level delivery is maintained within acceptable limits and conforms with the information presented in the GENOSYL DS Operator's Manual, Section 12.1.1, "Oxygen Dilution".
- NO Concentration Transients:NO concentration transients are ≤150% of mean concentration and as low as 0.0 ppm as long as the transient duration does not exceed 10% of the volumetric duration of the breath.

The testing performed demonstrated conformance with all specified requirements.

WARNING:

- ALWAYS use the GENOSYL DS in accordance with the indications, usage, contraindications, warnings, and precautions described in the GENOSYL prescribing information and labeling. Refer to latest approved prescribing information and labeling prior to use.
- The approved patient population for the GENOSYL DS as specified in the drug labeling for GENOSYL (nitric oxide) for inhalation, is limited to neonates. The GENOSYL DS is not intended to be used in other patient populations.

The following ventilators and non-invasive gas delivery systems have been validated for use with the GENOSYL DS. Validated ventilators were not tested with a nebulizer. See Section 1for assembly instructions for Injection Assembly with Adaptive Sensor and Mixer Assembly with Adaptive Sensor.

Table 3: Details of Validated Systems
Manufacturer | Model | Hospital [Refer to the Operator's Manual for additional Warnings, Cautions, and general information about use of the GENOSYL DS in the Hospital. Refer to Rev I, Section 7 for additional Warnings, Cautions, and information about use of the GENOSYL DS in the MR Scanner Room.] | External Transport [Refer to the Operator's Manual Rev I, Section 8 for additional Warnings, Cautions, and general information about use of the GENOSYL DS in External Transport.] | Anesthesia Gas Machine [Refer to the Operator's Manual Rev I, Section 9 for additional Warnings, Cautions, and general information about use of the GENOSYL DS with Anesthesia Gas Machines.] | Modes
Bio-Med Devices | Crossvent 2+ | • | • |  | - Cycle - CPAP
Bio-Med Devices | MVP-10 | • | • |  | - Cycle - CPAP
Dräger | Fabius GS, Fabius GS Premium, Fabius Tiro |  |  | • | - VC - PC - PS - SIMV/PS - Manual/ Spontaneous
Dräger | V500, VN 500, V600, VN 600, V800, VN800 | • |  |  | - VC-AC - VC-SIMV - VC-CMV - PC-AC - PC-SIMV - PC-CMV - PC-BIPAP - VC-MMV - PC-APRV - PC-PSV - SPN-CPAP/PS - SPN-CPAP/VS - SPN-PPS
GE | Aisys CS2 |  |  | • | - VCV - PCV - PCV-VG - PSVPro - CPAP+PSV - SIMV PCV - SIMV VCV - SIMV PCV-VG - Manual
Hamilton | C1/MR1 | • |  |  | - PCV+ - PSIMV+ - APVcmv - APVsimv/SIMV+ - ASV - DuoPAP - APRV - SPONT - NIV - NIV ST - nCPAPA - nCPAP PC
Hamilton | C6 | • |  |  | - APVcmv - APVsimv - PCV+ - PSIMV+ - DuoPAP - APRV - SPONT - ASV - NIV - NIV-ST - nCPAP-PS
Hamilton | G5 | • |  |  | - (S)CMV - P-CMV - P-SIMV - APVcmv - APVsimv - ASV - DuoPAP - APRV - SPONT - VS - NIV - NIV-ST - nCPAP-PS - SIMV
Hamilton | T1 | • | • |  | - PCV+ - PSIMV+ - APVcmv - APVsimv/SIMV+ - ASV - DuoPAP - APRV - SPONT - NIV - NIV ST - nCPAP - nCPAP PC
Puritan Bennett | 980 | • |  |  | - A/C PC - A/C VC - A/C VC+ - NIV AC PC - NIV AC VC - BiLevel - BiLevel PC PS - BiLevel PC TC - NIV CPAP - SPONT VS - NIV SPONT PS - SPONT TC - SPONT PAV+
Vyaire Medical Inc. | AVEA | • |  |  | - Volume A/C - Pressure A/C - Volume SIMV - Pressure SIMV - CPAP/PSV - PRVC A/C - PRVC SIMV - APRV/BiPhasic - TCPL A/C - TCPL SIMV - Nasal CPAP/IMV
Fisher & Paykel | Optiflow Jr 2 Breathing Circuit | • |  |  | N/A
Fisher and Paykel | Optiflow Breathing Circuit | • |  |  | N/A

Table 4: Validated Compatibility with and without Inline Mixer

At the lowest tested rate of 6 BPM, a Mixer may be used to reduce intra-breath dose variability as outlined in Table 4 below. Intra-breath dose variability was not observed at a respiratory rate of 60 BPM.

See Section 1for assembly instructions for Injection Assembly with Adaptive Sensor and Mixer Assembly with Adaptive Sensor.

VERO Biotech and GENOSYL are registered trademarks of VERO Biotech Inc.
© 2025 VERO Biotech. Printed in U.S.A. LBL-602503 Rev H JUNE 2025
Please read full prescribing information enclosed.
877.337.4118 | vero-biotech.com

INSTRUCTIONS FOR USE

USING THE GENOSYL®DELIVERY SYSTEM WITH AN ANESTHESIA GAS MACHINE

STEP 1: POWER ON THE GENOSYL DELIVERY SYSTEM
Refer to Operator's Manual Section 4.1 for detailed instructions.

1. Push circular power connectors into the back of the top and bottom Consoles.
2. Connect the main power cord to a grounded 120V electrical outlet.
3. Press the black rocker power switch on the back of each Console to the right (ON Position).
4. Press the silver power button, located in the top left corner of the front panel of each Console.

NOTE

Refer to Operator's Manual for use of the GENOSYL DS in the MR environment

STEP 2: REMOVE ALL GENOSYL DS COMPONENTS FROM PACKAGING
Refer to Operator's Manual Section 3.3 for detailed instructions.
This includes a Gas Injection Adapter, two Inline Breathing Circuit filters, Adaptive Sensor, Adaptive Sensor Cable, Sample Tee (if not already present in dual limb circuit), Manual Bag Adapter, Gas Lines and two Cassettes. [Specific use cases may require the use of an Inline Mixer which is used to mix the NO gas with the gas supplied by the AGM through a filter containing silica gel to provide intra-breath NO delivery for certain scenarios. Refer to Table 6 in the Operator's Manual for specific use cases and Section 3.4.2 for additional assembly instructions.]

STEP 3: ATTACH GAS LINES TO CONSOLES
Refer to Operator's Manual Section 3.5 for detailed instructions.

1. Push and twist clockwise the short Y-end of the NO Injection Line (red) to the "NO" port (red) on the front panel of both Consoles.
2. Push and twist clockwise the short Y-end of the Sample Line (blue) to the Gas Sample Port (blue) on the Water Trap attached to both Consoles.
3. Push and twist clockwise the end of the clear Manual Ventilation Line (clear) to the Manual Ventilation Port (clear) on the front of both Consoles.
4. Connect the Adaptive Sensor Cable to the Adaptive Sensor Port on the front of the Dosing Console.

STEP 4: ATTACH GAS LINES TO ANESTHESIA CIRCUIT INSPIRATORY LIMB
Refer to Operator's Manual Section 9.2 for detailed instructions.
An Inline Mixer may be required under some ventilation settings to assure NO dosing accuracy.
The settings where use of Inline Mixer is recommended are found in Section 9, Table 6 and instructions for the Inline Mixer Assembly with Adaptive Sensor are found in Section 3.4.2 of the Operator's Manual.

1. Check the expiration date for each Inline Breathing Circuit Filter to ensure use is within the expiration date.
2. Connect the Inline Breathing Circuit Filter to the Gas Injection Adapter (22 mm ID × 22 mm OD).
3. Connect the Adaptive Sensor to the inlet end of the Gas Injection Adapter (22mm ID × 22mm OD).
4. Attach the Injection Assembly with Adaptive Sensor to the Gas Injection Adapter on the Inspiratory Port on the AGM.
5. Attach the inspiratory limb of the breathing circuit to the Inline Breathing Circuit Filter. If the breathing circuit has a Sample Gas Tee inserted, ensure this limb of the circuit is attached to the Inline Breathing Circuit Filter.
6. Insert the Gas Sample Tee into the inspiratory limb of the breathing circuit, 6-12" from the patient wye.
7. Insert the Inline Breathing Circuit Filter between the Expiratory Port and expiratory limb. Skip this step if a bacterial filter is already present in the expiratory limb of the breathing circuit.
8. Attach the expiratory limb of the breathing circuit to the Inline Breathing Circuit Filter on the Expiratory Port on the Anesthesia Machine.
9. Push and twist clockwise the luer-lock collar from the NO injection line onto the NO injection port of the Gas Injection Adapter on the Injection Assembly.
10. Push and twist clockwise the luer-lock collar of the Stopcock on the Sample Line onto the Sampling Port of the Gas Sample Tee.
11. Connect the distal end of the Adaptive Sensor Cable to the Adaptive Sensor on the Injection Assembly.

NOTE

- Connections to various AGMS are unique to each manufacturer as well as their corresponding disposable circuits.
- A dual limb anesthesia breathing circuit should be used for iNO delivery with the GENOSYL DS.
- The GENOSYL DS Sample Line must be placed on the INSPIRATORY limb of the breathing circuit between 6 and 12 inches from the patient wye. If the sampling line is placed greater than 6 inches from the patient wye it minimizes the sampling of mixed inspired/expired gas concentrations and if placed less than 12 inches from the patient wye it ensures correct iNO and NO2measurement.

To ensure assembly setup is correct, refer to Figure 1. Anesthesia Machine Setup on reverse side.

STEP 5: ASSEMBLE MANUAL VENTILATION WITH THE GENOSYL DS
Refer to Operator's Manual Section 3.6 for detailed instructions.

1. Attach the barbed end of the Manual Ventilation Bag NO Adapter into the oxygen tubing from the oxygen source.
2. Attach the other end of the NO Adapter to the oxygen port on the side of the Manual Ventilation Bag.
3. Connect the Manual Ventilation Line (clear) to the NO Injection Port of the Manual Ventilation Bag NO Adapter.
4. Place the Manual Ventilation Assembly in a clean accessible place if needed for future use.

To ensure assembly setup is correct, refer to Figure 1. Anesthesia Machine Setup below.

WARNING

- ALWAYS use the GENOSYL DS in accordance with the indications, usage, contraindications, warnings, and precautions described in the GENOSYL prescribing information and labeling. Refer to latest approved prescribing information and labeling prior to use.
- ALWAYS use the Anesthesia Gas Machine (AGM) in accordance with the manufacturer's instructions.
- The approved patient population for the GENOSYL DS as specified in the drug labeling for GENOSYL (nitric oxide for inhalation (iNO)) is limited to neonates. The GENOSYL DS is not intended to be used in other patient populations.
- Ensure the Injection Assembly and the Gas Sample Tee are BOTH inserted on the inspiratory limb of the circuit.
- The flow out of the anesthesia gas machine via the INSPIRATORY breathing circuit limb must pass through the GENOSYL DS Gas Injection Assembly.
- The GENOSYL DS injects and samples gas from the patient respiratory circuit which may affect the triggering sensitivity of the anesthesia gas machine (AGM). ALWAYS ensure the trigger sensitivity of the AGM is checked after connecting the GENOSYL DS to the breathing circuit and starting iNO delivery or when the dose is changed, and adjust trigger sensitivity as necessary. Failure to do so may lead to AGM auto cycling or apnea alarm.
- ALWAYS ensure the patient disconnect and high-pressure alarms are used with the AGM.

CAUTION

- Pneumatic Nebulizers will dilute the delivered nitric oxide dose.
- The Adaptive Sensor is recommended for use with anesthesia gas machines (AGMs). When using an AGM without the Adaptive Sensor, transient dose excursions outside of the set NO dose may occur during Cassette transition, and changes in breathing circuit flow may cause fluctuations in measured levels of NO and NO2when using the manual ventilation bag integrated with the AGM.
- When using anesthesia gas machines, NO2levels may exceed 3.0 ppm when dosing ≥ 58 ppm NO into 100% FiO2, resulting in nitric oxide delivery interruption. Once sample value of NO2is below 3.0 ppm, the Console will auto resume delivery of NO at set dose.
- Rebreathing validation testing was performed with semi-closed breathing systems. Non-rebreathing validation testing was performed with semi-open breathing systems. The GENOSYL DS has not been evaluated with fully open or fully closed anesthesia breathing systems.

NOTE

- The GENOSYL DS performs as specified in this Operator's Manual independent of anesthetic agent, anesthetic agent concentration, and fresh gas flow rate.
- Changes in the AGM ventilator settings, fresh gas flow rate, or pushing the Oxygen Flush button by the user may cause brief transient changes in the measured NO value.
- Use of an Adaptive Sensor is recommended for use with AGMs. If not using an Adaptive Sensor:
  - And using rebreathing fresh gas flow rates, it is recommended that the < 2.5 LPM Total Flow setting be selected.
  - And using non-rebreathing fresh gas flow rates, it is recommended that the Total Flow selection based on the minute volume be selected.
- When using the manual ventilation bag integrated with the AGM, nitric oxide can be delivered by leaving the Console in Primary Dosing Mode. Nitric oxide will be delivered through the Injection Assembly into the anesthesia gas circuit.
- In the event of anesthesia gas machine failure, NO delivery can be continued using Manual Dosing Mode on the GENOSYL DS with a manual bag connected to the manual ventilation port on the front of the Console and an alternative gas source than the AGM.

INSERTING A CASSETTE
Refer to Operator's Manual Section 4.2 for detailed instructions.

STEP 1: CHECK THE CASSETTE

1. Remove Cassettes from packaging.
2. Check the expiration date for each Cassette to ensure use is within the expiration date.
3. Confirm Cassette status indicator on each Cassette is blue.

STEP 2: INSERT CASSETTE INTO THE CONSOLE

1. Open the Cassette Access Door and insert two Cassettes into the Dosing Console and at least one Cassette into the Back-up Console. Push until it clicks.

STEP 3: COMPLETE WATER TRAP / SAMPLE LINE LEAK TEST

1. Follow on-screen instructions on both Consoles to complete Water Trap / Sample Line Leak Test.

INITIATING A NITRIC OXIDE DOSE
Refer to Operator's Manual Section 5.1.1 for detailed instructions.

STEP 1: INITIATE NITRIC OXIDE ADMINISTRATION

1. Press the gray Set button on the display screen.

1. Enter the prescribed dose in ppm on the electronic keypad.
2. Press OK to confirm entry.

ADJUSTING THE NITRIC OXIDE DOSE
Refer to Operator's Manual Section 5.2.1 for detailed instructions.

STEP 1: SET FLOW

1. Press the gray "Set" button to access the electronic keypad on the display screen on the Dosing Console.
2. Enter the prescribed ppm dose using the electronic keypad.
3. Press "OK" to confirm the dose and to start dosing administration.

MANUAL VENTILATION MODE USING EXTERNAL RESUSCITATION BAG
Refer to Operator's Manual Section 5.4.1 for detailed instructions.

WARNING

- ALWAYS ensure that the manual flow displayed on the Console matches the flow set into the resuscitation bag. Incorrect flow settings may result in an incorrect estimation of NO delivery. If the flow into the manual equipment is too low, there is risk of overdosing the patient with NO.
- ALWAYS squeeze the bag several times, after starting fresh gas flow, to empty residual gas in the bag prior to using the System to ventilate a patient. Failure to do so could result in higher NO2levels being delivered to the patient.
- ALWAYS use the smallest bag adequate to deliver the desired tidal volume. Failure to do so could result in higher NO2levels being delivered to the patient.
- ONLY use a manual resuscitation bag with the GENOSYL DS for a short time (e.g., less than one hour) when on battery only. Otherwise, the System may shut off and may result in injury or death.

STEP 1: SWITCHING TO MANUAL DOSING MODE

1. Ensure the oxygen flow source is set appropriately or adjust as needed.
2. Press the button "Switch to Manual" on the Dosing Console.
3. Press Confirm to switch to Manual Dosing Mode.

WARNING

If the dilution flow rate displayed on the screen does not match the wall source, then the estimated NO may be inaccurate.

STEP 2: SWITCHING BACK TO PRIMARY DOSING MODE

1. Press the "Switch to Primary" button at the top of the Manual Dosing Mode screen.

1. Press "Confirm" to start dosing or "Cancel" to cancel.

GAS SAMPLING DURING AEROSOL DELIVERY
Refer to Operator's Manual Section 3.8 for detailed instructions.

1. Place the medication nebulizer downstream of the Gas Sample Tee on the inspiratory limb. | 1. Insert and connect the Sample Line Filter between the Sample Line and blue Stopcock. Refer to Operator's Manual Section 3.5.3 for detailed instructions to connect a Sample Line Filter.

 | NOTE |  | NOTE
 | This placement avoids contamination of the sample system and prevents Line Occlusion Alarm from occurring. |  | Replace filter after each treatment period. Change the filter if necessary due to Line Occlusion Alarm.

CAUTION

Pneumatic Nebulizers will dilute the delivered nitric oxide dose.

CONSOLE USE AS A BACK-UP
Refer to Operator's Manual Section 5.5 for detailed instructions.

1. Press the "Set" button on the Back-up Console which will display the NO dose electronic keypad and Flow Selection menu.
2. Confirm Dose and Total Flow range is appropriately selected.

1. Press "OK" to confirm entry
2. Connect the Adaptive Sensor Cable to the front of the new Dosing Console.

POWERING DOWN THE SYSTEM
Refer to Operator's Manual Section 6.1 for detailed instructions.

STEP 1: POWERING DOWN THE SYSTEM

1. Press the gray "Set" button to access the electronic keypad on the display screen.
2. Set the dose to "0" using the electronic keyboard.
3. Press "OK" to confirm the entry.
4. If the Settings Tab is not displayed, press the "Menu" tab to access the sub-level tabs.

1. Press the "Settings" tab on the display menu.
2. Press the red "System Shutdown" icon.

1. Review on-screen prompt.
2. Press "Confirm" to confirm shutdown.
3. Wait until the Console shuts down, the display screen appears blank, and the Console emits an audible beep.

STEP 2: REMOVE THE CASSETTE

1. Open the Cassette Access Door.
2. Remove the Cassettes by pulling the Cassette straight out.
3. Dispose of the inerted Cassette per hospital policy.

NOTE

The Console will inert any remaining contents from a dosing Cassette upon ejection, rendering it unusable. If a Cassette has only been preheated, and not used for dosing, the contents have not been inerted and it can still be used. The Cassette State Window will remain blue on Cassettes that have not been inerted.

EMPTY AND REPLACE WATER TRAP
Refer to Operator's Manual Section 11.4 for detailed instructions.

STEP 1: EMPTY THE WATER TRAP

1. Remove Water Traps from both Consoles by lifting latch and pulling the base of the Water Trap away from the Console.
2. Remove the lids by pulling the lid away from the base.
3. Empty the liquid contents.
4. Reattach the lids by pushing back onto base.
5. Slide the Water Traps back on both Consoles until they click into place.

CRITICAL ALARM TROUBLESHOOTING
Refer to Operator's Manual Section 10 for detailed instructions.

ALARM CONDITION

TROUBLE SHOOTING

LINE OCCLUSION (Sample)
Message Box:
None
Banner:

In this fallback mode, the Console will continue delivering nitric oxide in an open loop mode at the last commanded dose until the line occlusion is resolved.

1. Ensure blue Sample Line Stopcock is in the open position.
2. Remove Sample Line Filter, replace if needed.
3. Empty Water Tap.
4. If occlusion persists after emptying, replace Water Trap.
5. Inspect entire length of blue sample line for kinks or occlusions.
6. Replace gas lines if kink or occlusion cannot be resolved.
7. If issue is still not resolved, switch over to Back-up Console.
8. Contact Technical Support.

WATER TRAP NOT DETECTED
Message Box:

Banner:

In this fallback mode, the console will continue delivering nitric oxide in an open loop mode at the last commanded dose until the water trap is replaced and the leak check is passed.

1. Re-seat Water Trap.
2. Insert new Water Trap.
3. Switch over to Back-up Console.
4. Call Technical Support.

LOW NO ALARM
Message Box:
None
Banner:

1. Verify GENOSYL DS gas line connections are tight by loosening then retightening each connection on the red injection and blue sample lines.
2. Verify proper placement of Injection Assembly and Sample adapter within the respiratory circuit.
3. Ensure gas sample tee is placed 6 to 12 inches from the patient wye adapter.
4. Replace adapters that have evidence of excessive condensation.
5. Check the respiratory circuit for the presence of leaks.
6. If not using an Adaptive Sensor, confirm total flow range is properly selected.
7. Allow time for the sensor measurement to adjust while completing the next steps.
8. Push on Cassette to ensure it is fully seated.
9. Empty Water Trap. Replace Water Trap if necessary.
10. If Cassette is depleted, insert a second Cassette if not already present. If auto transition does not occur, switch to Back-up Console.
11. Ensure dose and flow are set within specifications. (see Operator's Manual Section 12.1.4) Liters per minute multiplied by ppm should not exceed 800. (Example 40 LPM × 20ppm = 800)
12. Go to alarms screen and check the NO alarm setting. Set the alarm to the desired setting.
13. If sensor measurement does not adjust, switch over to Back-up Console.
14. Contact Technical Support.

HIGH NO ALARM
Message Box:
None
Banner:

1. Verify flow is present in the patient's respiratory circuit.
2. Allow time for the sensor measurement to adjust while completing the next steps.
3. Verify GENOSYL DS gas line connections are tight by loosening then retightening each connection on the red injection and blue sample lines.
4. Verify proper placement of injection assembly and sample adapter within the respiratory circuit.
5. Replace adapters that have evidence of excessive condensation.
6. Go to the Alarms screen and check the NO alarm setting. Set alarm to the desired setting.
7. If the sensor measurement does not adjust, switch to Back-up Console.
8. Contact Technical Support.

HIGH NO2ALARM
Message Box:
None
Banner:

1. Verify flow is present in the patient's respiratory circuit.
2. Consider increasing bias flow, if applicable
3. Allow time for the sensor measurement to adjust while completing the next steps.
4. Verify GENOSYL DS gas line connections are tight by loosening then retightening each connection on the red injection and blue sample lines.
5. Verify proper placement of injection assembly and sample adapter within the respiratory circuit.
6. Replace adapters that have evidence of excessive condensation.
7. Go to the Alarms screen and check the NO2alarm setting. Set alarm to the desired setting.
8. If the sensor measurement does not adjust, switch to Back-up Console
9. Contact Technical Support.

This section contains troubleshooting instructions for common high priority alarms and messages and common possible causes in the OR setting of use. For other high priority alarms and messages and possible causes please refer to the Operator's Manual Section 10.3.

For technical support, contact the Partnership365™ Care Team at 1.877.337.4118

VERO Biotech and GENOSYL are registered trademarks of VERO Biotech Inc.
© 2025 VERO Biotech Inc. All rights reserved. MMC-602936 Rev. B June 2025
Please refer to full Prescribing Information and Operators Manual
vero-biotech.com | 1.877.337.4118

aarc
ZENITH AWARD
2024

PRINCIPAL DISPLAY PANEL - 216 L Cartridge Label

GENOSYL®(nitric oxide)
for inhalation

Recommended dosage: see prescribing information

For use with GENOSYL Delivery System only

LOT
Z-XXXX-YYYY

SN
ZZXXZXXX

EXP
YYYY-MM-DD

VĒRO
BIOTECH